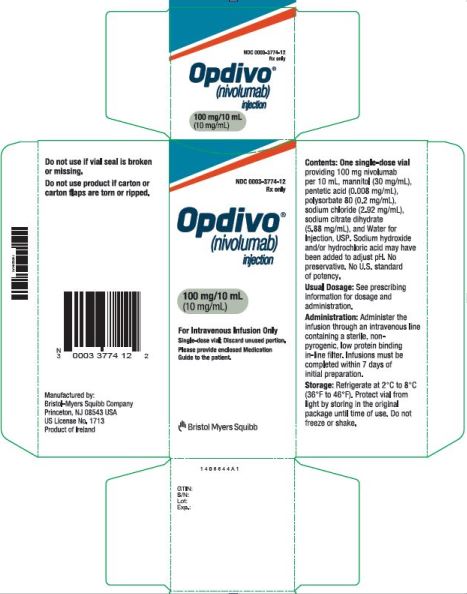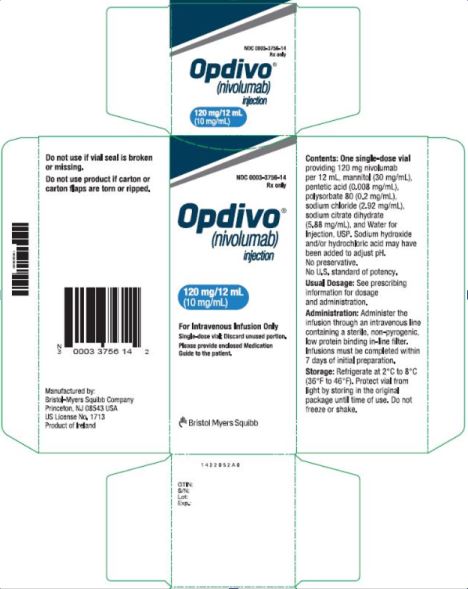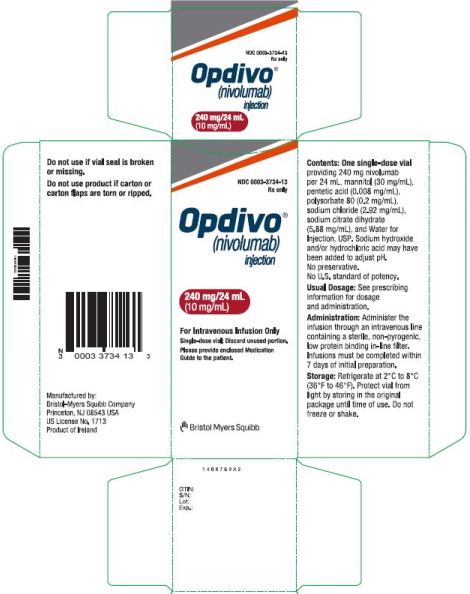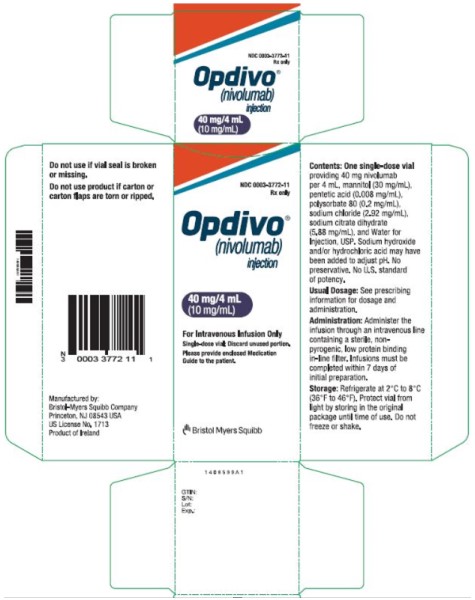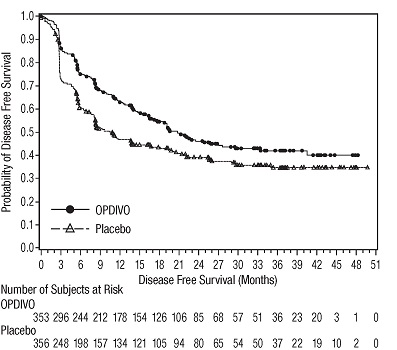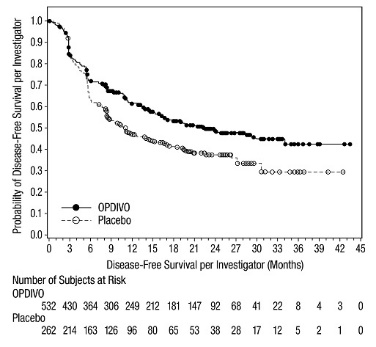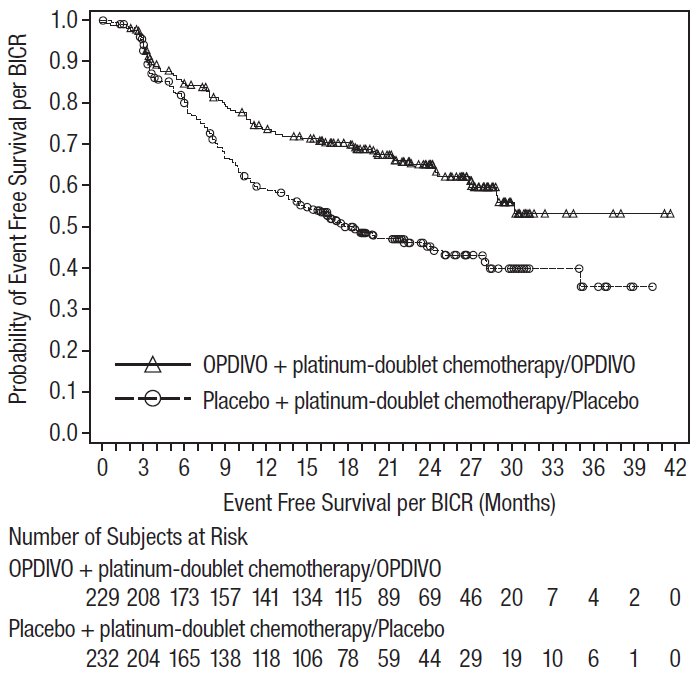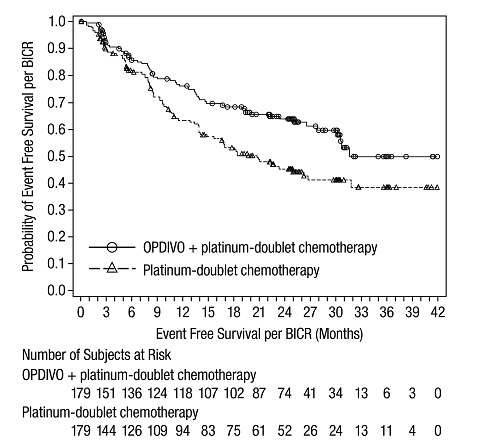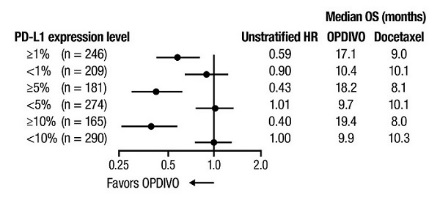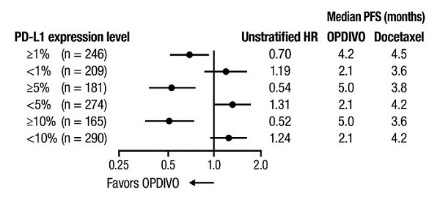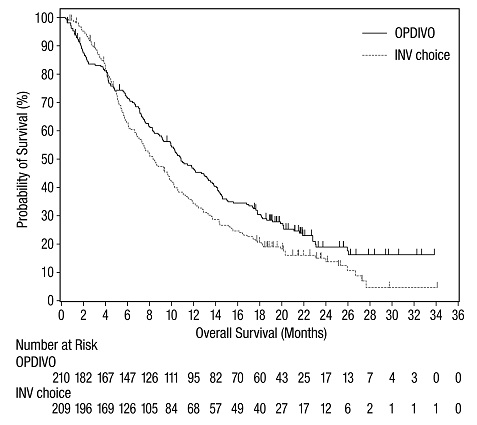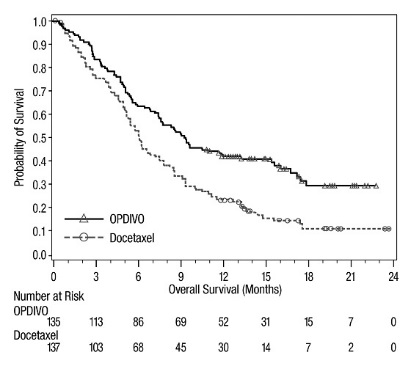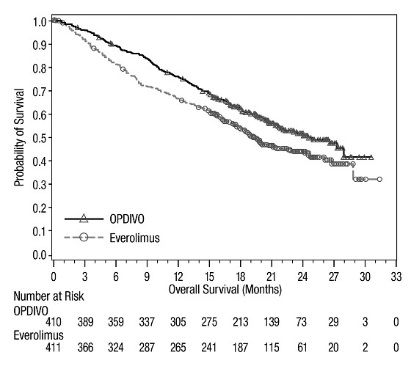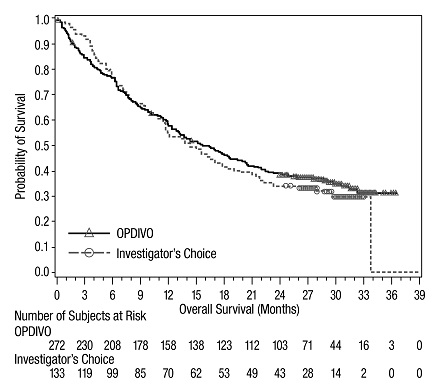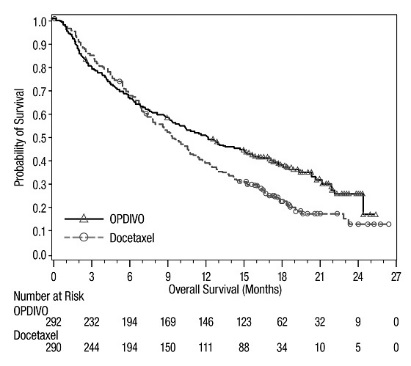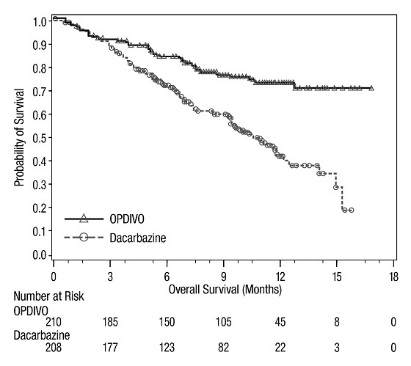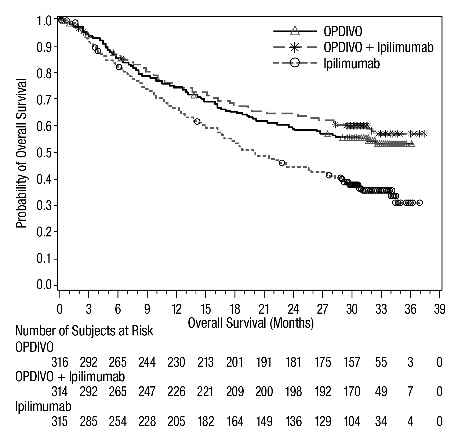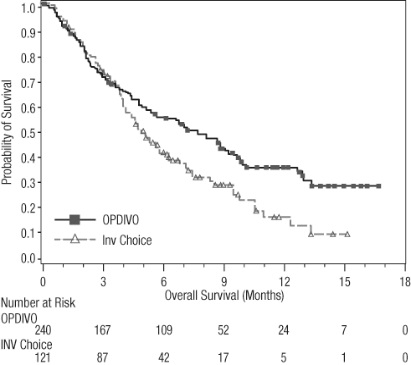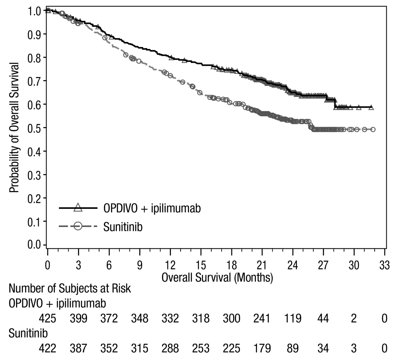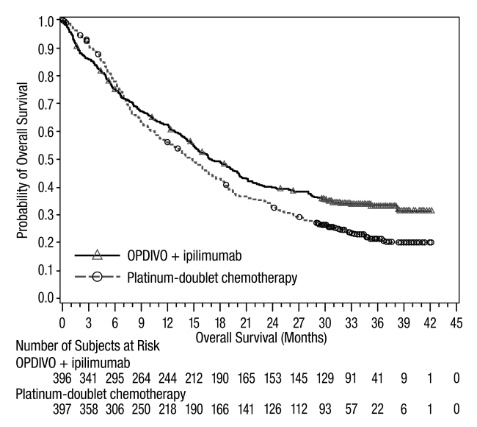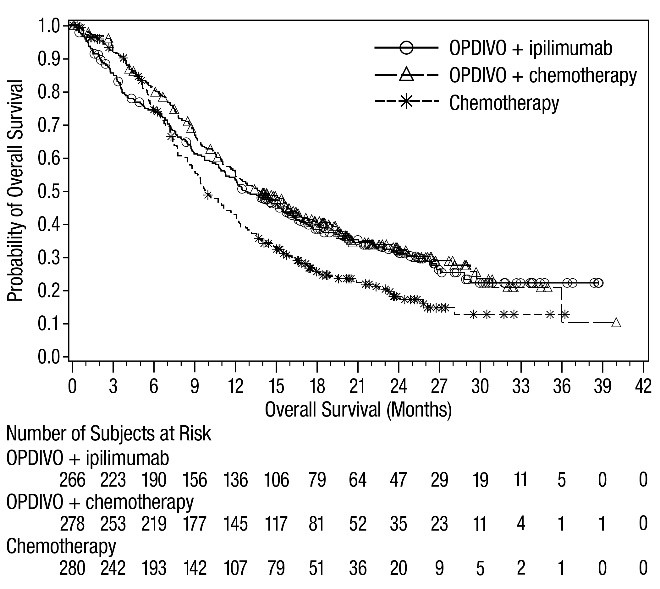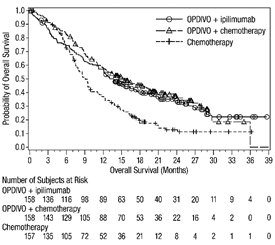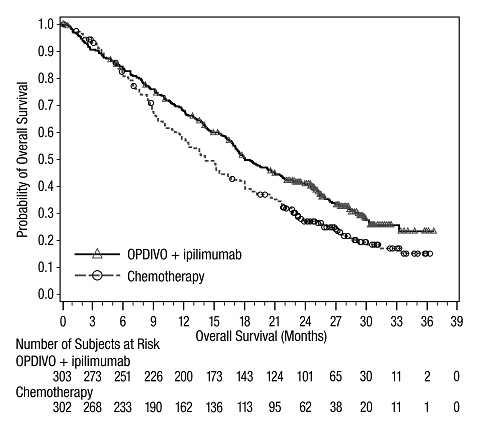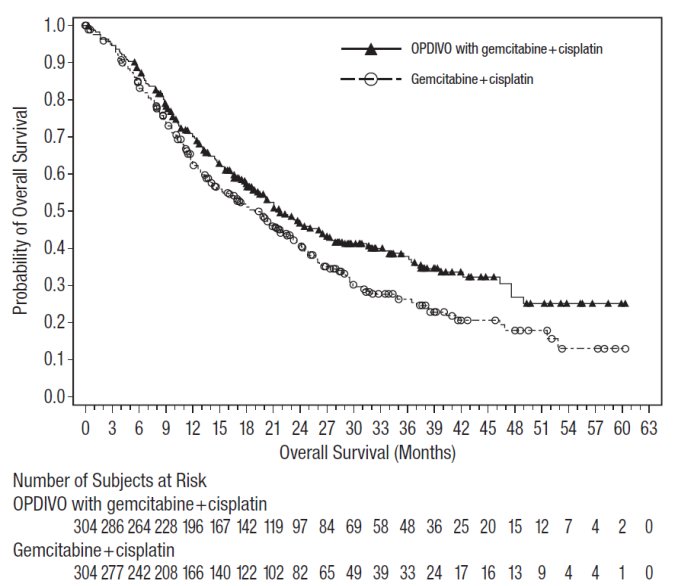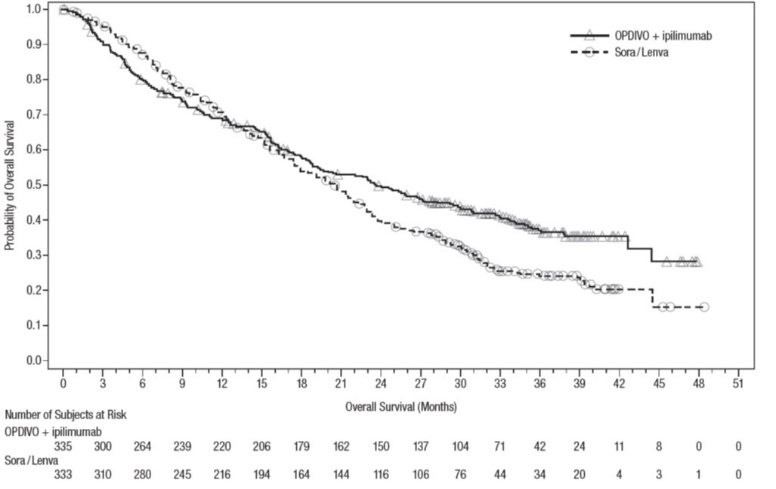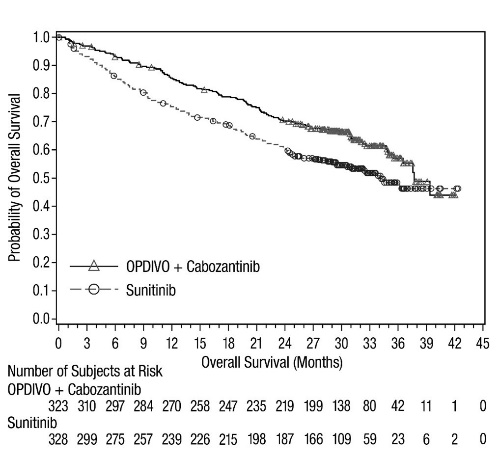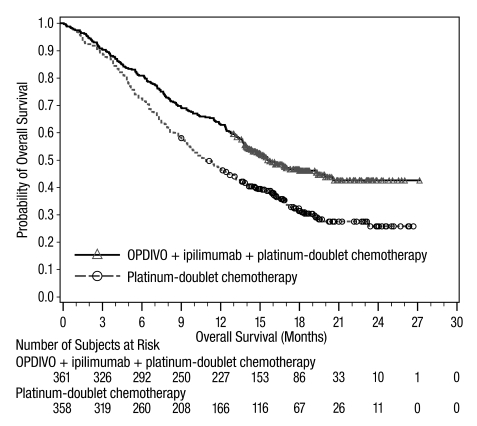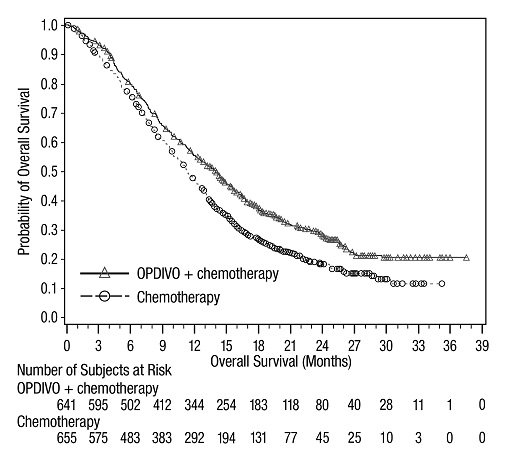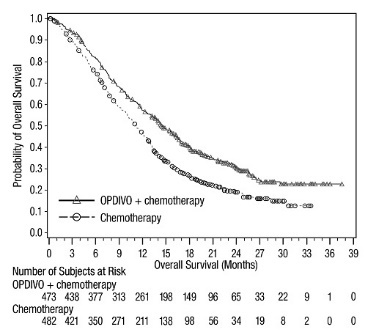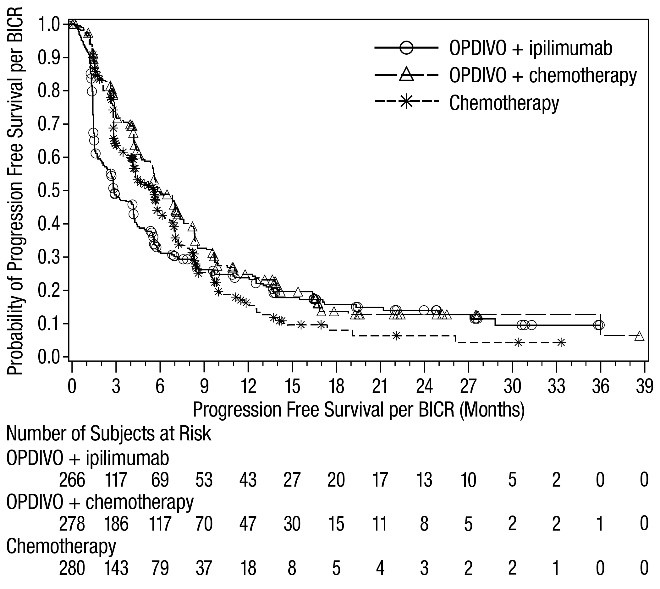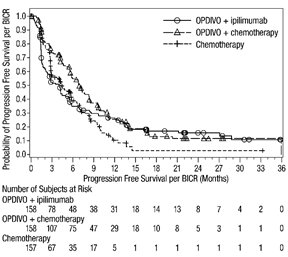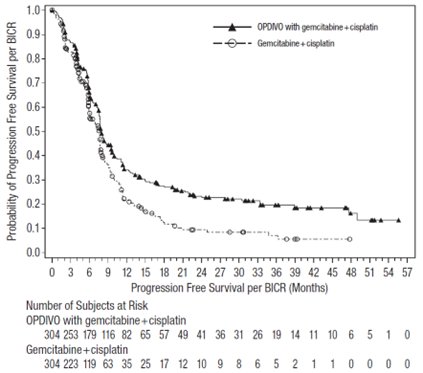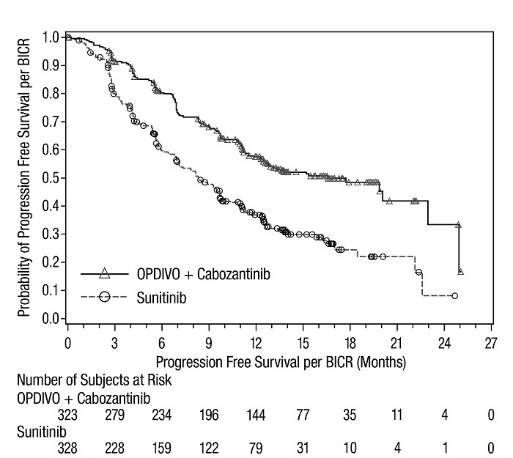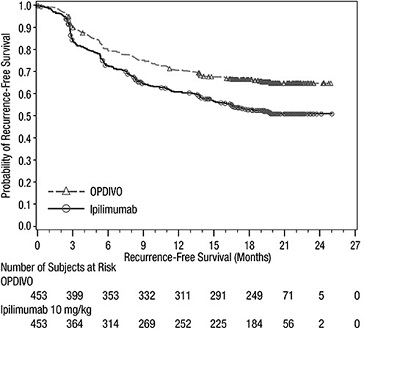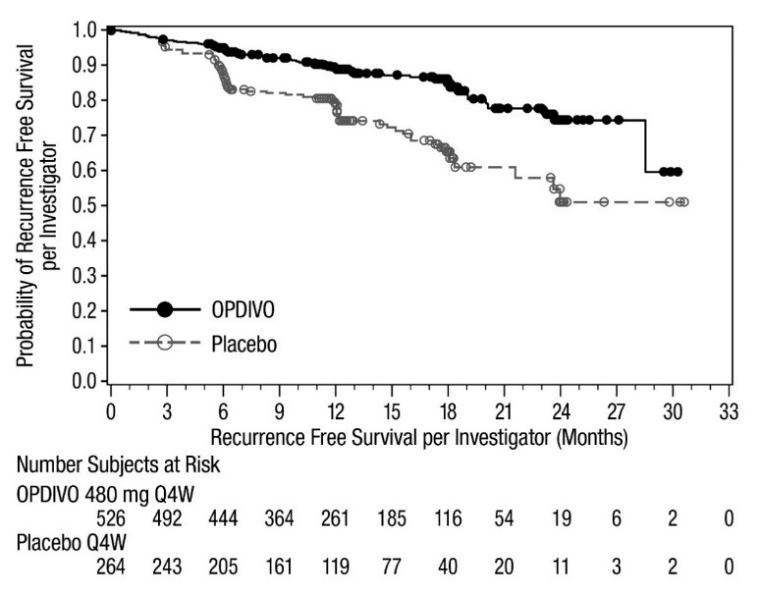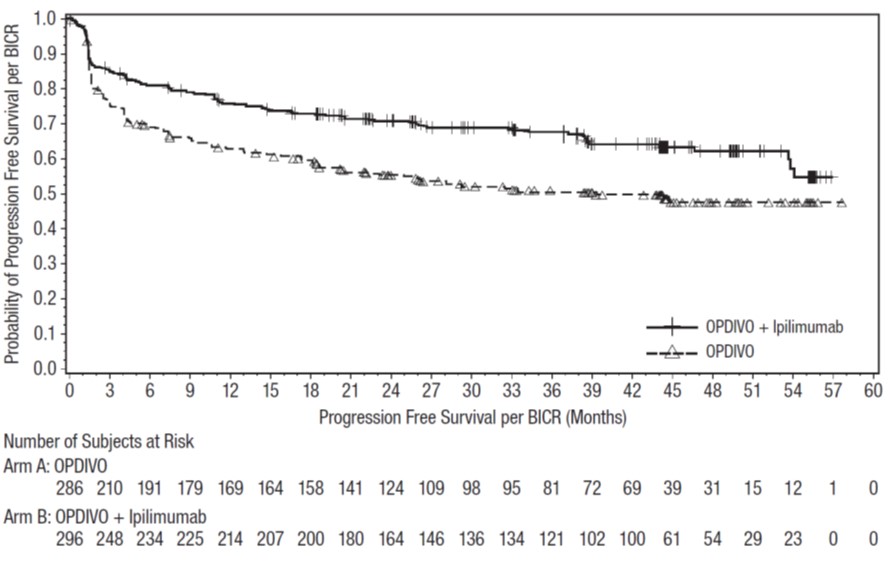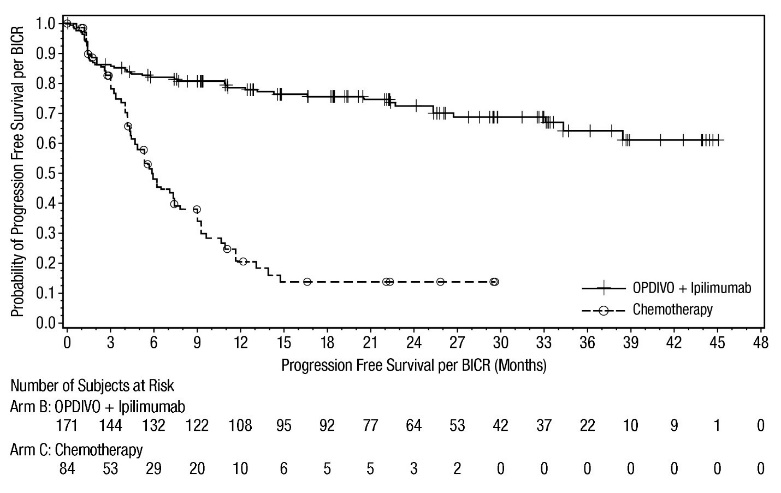 DRUG LABEL: OPDIVO
NDC: 0003-3772 | Form: INJECTION
Manufacturer: E.R. Squibb & Sons, L.L.C.
Category: prescription | Type: HUMAN PRESCRIPTION DRUG LABEL
Date: 20250701

ACTIVE INGREDIENTS: NIVOLUMAB 10 mg/1 mL
INACTIVE INGREDIENTS: MANNITOL 30 mg/1 mL; PENTETIC ACID 0.008 mg/1 mL; POLYSORBATE 80 0.2 mg/1 mL; SODIUM CHLORIDE 2.92 mg/1 mL; TRISODIUM CITRATE DIHYDRATE 5.88 mg/1 mL; WATER; HYDROCHLORIC ACID; SODIUM HYDROXIDE

HIGHLIGHTS OF PRESCRIBING INFORMATION

These highlights do not include all the information needed to use OPDIVO safely and effectively. See full prescribing information for OPDIVO.
OPDIVO® (nivolumab) injection, for intravenous use
Initial U.S. Approval: 2014

RECENT MAJOR CHANGES

Indications and Usage (1) | 5/2025
Dosage and Administration (2) | 5/2025

1 INDICATIONS AND USAGE

OPDIVO is a programmed death receptor-1 (PD-1)-blocking antibody indicated for the treatment of:

Melanoma

- adult and pediatric (12 years and older) patients with unresectable or metastatic melanoma, as a single agent or in combination with ipilimumab. (1.1)
- for the adjuvant treatment of adult and pediatric patients 12 years and older with completely resected Stage IIB, Stage IIC, Stage III, or Stage IV melanoma. (1.2)

Non-Small Cell Lung Cancer (NSCLC)

- adult patients with resectable (tumors ≥4 cm or node positive) non-small cell lung cancer in the neoadjuvant setting, in combination with platinum-doublet chemotherapy. (1.3)
- adult patients with resectable (tumors ≥4 cm or node positive) non-small cell lung cancer and no known EGFR mutations or ALK rearrangements, for neoadjuvant treatment, in combination with platinum-doublet chemotherapy, followed by single-agent OPDIVO as adjuvant treatment after surgery. (1.4)
- adult patients with metastatic non-small cell lung cancer expressing PD‑L1 (≥1%) as determined by an FDA-approved test, with no EGFR or ALK genomic tumor aberrations, as first-line treatment in combination with ipilimumab. (1.5)
- adult patients with metastatic or recurrent non-small cell lung cancer with no EGFR or ALK genomic tumor aberrations as first-line treatment, in combination with ipilimumab and 2 cycles of platinum-doublet chemotherapy. (1.5)
- adult patients with metastatic non-small cell lung cancer and progression on or after platinum-based chemotherapy. Patients with EGFR or ALK genomic tumor aberrations should have disease progression on FDA-approved therapy for these aberrations prior to receiving OPDIVO. (1.5)

Malignant Pleural Mesothelioma

- adult patients with unresectable malignant pleural mesothelioma, as first-line treatment in combination with ipilimumab. (1.6)

Renal Cell Carcinoma (RCC)

- adult patients with intermediate or poor risk advanced renal cell carcinoma, as a first-line treatment in combination with ipilimumab. (1.7)
- adult patients with advanced renal cell carcinoma, as a first-line treatment in combination with cabozantinib. (1.7)
- adult patients with advanced renal cell carcinoma who have received prior anti-angiogenic therapy. (1.7)

Classical Hodgkin Lymphoma (cHL)

- adult patients with classical Hodgkin lymphoma that has relapsed or progressed aftera: (1.8)
  - autologous hematopoietic stem cell transplantation (HSCT) and brentuximab vedotin, or
  - 3 or more lines of systemic therapy that includes autologous HSCT.

Squamous Cell Carcinoma of the Head and Neck (SCCHN)

- adult patients with recurrent or metastatic squamous cell carcinoma of the head and neck with disease progression on or after a platinum-based therapy. (1.9)

Urothelial Carcinoma

- adjuvant treatment of adult patients with urothelial carcinoma (UC) who are at high risk of recurrence after undergoing radical resection of UC. (1.10)
- adult patients with unresectable or metastatic urothelial carcinoma, as first-line treatment in combination with cisplatin and gemcitabine. (1.10)
- adult patients with locally advanced or metastatic urothelial carcinoma who:
  - have disease progression during or following platinum-containing chemotherapy.
  - have disease progression within 12 months of neoadjuvant or adjuvant treatment with platinum-containing chemotherapy. (1.10)

Colorectal Cancer

- adult and pediatric (12 years and older) patients with unresectable or metastatic microsatellite instability-high (MSI-H) or mismatch repair deficient (dMMR) colorectal cancer (CRC) in combination with ipilimumab. (1.11)
- adult and pediatric (12 years and older) patients with microsatellite instability-high (MSI-H) or mismatch repair deficient (dMMR) metastatic colorectal cancer that has progressed following treatment with a fluoropyrimidine, oxaliplatin, and irinotecan. (1.11)

Hepatocellular Carcinoma (HCC)

- adult patients with unresectable or metastatic hepatocellular carcinoma (HCC), as a first-line treatment in combination with ipilimumab. (1.12)
- in combination with ipilimumab in adult patients with unresectable or metastatic HCC who have been previously treated with sorafenib. (1.12)

Esophageal Cancer

- adult patients with completely resected esophageal or gastroesophageal junction cancer with residual pathologic disease, who have received neoadjuvant chemoradiotherapy (CRT). (1.13)
- adult patients with unresectable advanced or metastatic esophageal squamous cell carcinoma as first-line treatment in combination with fluoropyrimidine- and platinum‑containing chemotherapy whose tumors express PD-L1 (≥1). (1.13)
- adult patients with unresectable advanced or metastatic esophageal squamous cell carcinoma as first-line treatment in combination with ipilimumab whose tumors express PD-L1 (≥1). (1.13)
- adult patients with unresectable advanced, recurrent or metastatic esophageal squamous cell carcinoma (ESCC) after prior fluoropyrimidine- and platinum-based chemotherapy. (1.13)

Gastric Cancer, Gastroesophageal Junction Cancer, and Esophageal Adenocarcinoma

- adult patients with advanced or metastatic gastric cancer, gastroesophageal junction cancer, and esophageal adenocarcinoma whose tumors express PD-L1 (≥1) in combination with fluoropyrimidine- and platinum-containing chemotherapy. (1.14)

a This indication is approved under accelerated approval based on overall response rate and duration of response. Continued approval for this indication may be contingent upon verification and description of clinical benefit in confirmatory trials.

2 DOSAGE AND ADMINISTRATION

- Administer by intravenous infusion after dilution based upon recommended infusion rate for each indication. (2)
- Unresectable or metastatic melanoma
  - Adult and pediatric patients weighing 40 kg or greater: 240 mg every 2 weeks or 480 mg every 4 weeks. (2.2)
  - Pediatric patients weighing less than 40 kg: 3 mg/kg every 2 weeks or 6 mg/kg every 4 weeks. (2.2)
  - Adult and pediatric patients weighing 40 kg or greater: 1 mg/kg followed by ipilimumab 3 mg/kg on the same day every 3 weeks for 4 doses, then 240 mg every 2 weeks or 480 mg every 4 weeks. (2.2)
  - Pediatric patients weighing less than 40 kg: 1 mg/kg followed by ipilimumab 3 mg/kg on the same day every 3 weeks for 4 doses, then 3 mg/kg every 2 weeks or 6 mg/kg every 4 weeks. (2.2)
- Adjuvant treatment of melanoma
  - Adult and pediatric patients weighing 40 kg or greater: 240 mg every 2 weeks or 480 mg every 4 weeks. (2.2)
  - Pediatric patients weighing less than 40 kg: 3 mg/kg every 2 weeks or 6 mg/kg every 4 weeks. (2.2)
- Neoadjuvant treatment of resectable (tumors ≥4 cm or node positive) non-small cell lung cancer
  - 360 mg with platinum-doublet chemotherapy on the same day every 3 weeks for 3 cycles. (2.2)
- Neoadjuvant and adjuvant treatment of resectable non-small cell lung cancer
  - 360 mg with platinum-doublet chemotherapy on the same day every 3 weeks for up to 4 cycles, then continued as single-agent OPDIVO 480 mg every 4 weeks after surgery for up to 13 cycles (~1 year). (2.2)
- Metastatic non-small cell lung cancer
  - 360 mg every 3 weeks with ipilimumab 1 mg/kg every 6 weeks. (2.2)
  - 360 mg every 3 weeks with ipilimumab 1 mg/kg every 6 weeks and 2 cycles of platinum-doublet chemotherapy. (2.2)
  - 240 mg every 2 weeks or 480 mg every 4 weeks. (2.2)
- Malignant pleural mesothelioma
  - 360 mg every 3 weeks with ipilimumab 1 mg/kg every 6 weeks. (2.2)
- Advanced renal cell carcinoma
  - 3 mg/kg followed by ipilimumab 1 mg/kg on the same day every 3 weeks for 4 doses, then 240 mg every 2 weeks or 480 mg every 4 weeks. (2.2)
  - 240 mg every 2 weeks or 480 mg every 4 weeks administered in combination with cabozantinib 40 mg once daily without food. (2.2)
  - 240 mg every 2 weeks or 480 mg every 4 weeks. (2.2)
- Classical Hodgkin lymphoma
  - 240 mg every 2 weeks or 480 mg every 4 weeks. (2.2)
- Recurrent or metastatic squamous cell carcinoma of the head and neck
  - 240 mg every 2 weeks or 480 mg every 4 weeks. (2.2)
- Adjuvant treatment of urothelial carcinoma
  - 240 mg every 2 weeks or 480 mg every 4 weeks. (2.2)
- First-line unresectable or metastatic urothelial carcinoma
  - 360 mg every 3 weeks with cisplatin and gemcitabine on the same day for up to 6 cycles, then 240 mg every 2 weeks or 480 mg every 4 weeks. (2.2)
- Previously treated locally advanced or metastatic urothelial carcinoma
  - 240 mg every 2 weeks or 480 mg every 4 weeks. (2.2)
- Microsatellite instability-high (MSI-H) or mismatch repair deficient (dMMR) metastatic colorectal cancer
  - Adult and pediatric patients weighing 40 kg or greater: 240 mg followed by ipilimumab 1 mg/kg on the same day every 3 weeks for a maximum of 4 doses, then 240 mg every 2 weeks or 480 mg every 4 weeks. (2.2)
  - Pediatric patients weighing less than 40 kg: 3 mg/kg followed by ipilimumab 1 mg/kg on the same day every 3 weeks for a maximum of 4 doses, then 3 mg/kg every 2 weeks or 6 mg/kg every 4 weeks. (2.2)
- Microsatellite instability-high (MSI-H) or mismatch repair deficient (dMMR) metastatic colorectal cancer that has progressed following prior treatment for metastatic disease.
  - Adult and pediatric patients weighing 40 kg or greater: 240 mg every 2 weeks or 480 mg every 4 weeks. (2.2)
  - Pediatric patients weighing less than 40 kg: 3 mg/kg every 2 weeks. (2.2)
- Hepatocellular carcinoma
  - 1 mg/kg followed by ipilimumab 3 mg/kg on the same day every 3 weeks for 4 doses, then 240 mg every 2 weeks or 480 mg every 4 weeks. (2.2)
- Adjuvant treatment of resected esophageal or gastroesophageal cancer
  - 240 mg every 2 weeks or 480 mg every 4 weeks for total treatment duration of 1 year. (2.2)
- Esophageal squamous cell carcinoma
  - 240 mg every 2 weeks or 480 mg every 4 weeks in combination with chemotherapy regimen of fluoropyrimidine- and platinum-containing chemotherapy. (2.2)
  - 3 mg/kg every 2 weeks or 360 mg every 3 weeks with ipilimumab 1 mg/kg every 6 weeks. (2.2)
  - 240 mg every 2 weeks or 480 mg every 4 weeks. (2.2)
- Gastric cancer, gastroesophageal junction cancer, and esophageal adenocarcinoma (GC, GEJC, or EAC)
  - 360 mg every 3 weeks with fluoropyrimidine- and platinum-containing chemotherapy every 3 weeks. (2.2)
  - 240 mg every 2 weeks with fluoropyrimidine- and platinum-containing chemotherapy every 2 weeks. (2.2)
- See full Prescribing Information for preparation and administration instructions and dosage modifications for adverse reactions.

3 DOSAGE FORMS AND STRENGTHS

- Injection: 40 mg/4 mL (10 mg/mL), 100 mg/10 mL (10 mg/mL), 120 mg/12 mL (10 mg/mL), and 240 mg/24 mL (10 mg/mL) solution in a single-dose vial. (3)

4 CONTRAINDICATIONS

- None. (4)

5 WARNINGS AND PRECAUTIONS

- Immune-Mediated Adverse Reactions: (5.1)
  - Immune-mediated adverse reactions, which may be severe or fatal, can occur in any organ system or tissue, including the following: immune-mediated pneumonitis, immune-mediated colitis, immune-mediated hepatitis and hepatotoxicity, immune-mediated endocrinopathies, immune-mediated dermatologic adverse reactions, and immune-mediated nephritis and renal dysfunction.
  - Monitor for early identification and management. Evaluate liver enzymes, creatinine, and thyroid function at baseline and periodically during treatment.
  - Withhold or permanently discontinue based on severity and type of reaction. (2.3)
- Infusion-related reactions: Interrupt, slow the rate of infusion, or permanently discontinue OPDIVO based on severity of reaction. (5.2)
- Complications of allogeneic HSCT: Fatal and other serious complications can occur in patients who receive allogeneic HSCT before or after being treated with a PD-1/PD-L1 blocking antibody. (5.3)
- Embryo-Fetal toxicity: Can cause fetal harm. Advise females of reproductive potential of potential risk to a fetus and to use effective contraception. (5.4, 8.1, 8.3)
- Treatment of patients with multiple myeloma with a PD-1 or PD-L1 blocking antibody in combination with a thalidomide analogue plus dexamethasone is not recommended outside of controlled clinical trials. (5.5)

6 ADVERSE REACTIONS

Most common adverse reactions (incidence ≥20%) in patients were:

- As a single agent: fatigue, rash, musculoskeletal pain, pruritus, diarrhea, nausea, asthenia, cough, dyspnea, constipation, decreased appetite, back pain, arthralgia, upper respiratory tract infection, pyrexia, headache, abdominal pain, vomiting, and urinary tract infection. (6.1)
- In combination with ipilimumab: fatigue, diarrhea, rash, pruritus, nausea, musculoskeletal pain, pyrexia, cough, decreased appetite, vomiting, abdominal pain, dyspnea, upper respiratory tract infection, arthralgia, headache, hypothyroidism, constipation, decreased weight, and dizziness. (6.1)
- In combination with platinum-doublet chemotherapy: nausea, fatigue, musculoskeletal pain, constipation, decreased appetite, rash, vomiting, and peripheral neuropathy. (6.1)
- In combination with ipilimumab and platinum-doublet chemotherapy: fatigue, musculoskeletal pain, nausea, diarrhea, rash, decreased appetite, constipation, and pruritus. (6.1)
- In combination with cabozantinib: diarrhea, fatigue, hepatotoxicity, palmar-plantar erythrodysesthesia syndrome, stomatitis, rash, hypertension, hypothyroidism, musculoskeletal pain, decreased appetite, nausea, dysgeusia, abdominal pain, cough, and upper respiratory tract infection. (6.1)
- In combination with fluoropyrimidine- and platinum-containing chemotherapy: nausea, peripheral neuropathy, decreased appetite, fatigue, constipation, stomatitis, diarrhea, vomiting, abdominal pain, and musculoskeletal pain. (6.1)

To report SUSPECTED ADVERSE REACTIONS, contact Bristol-Myers Squibb at 1-800-721-5072 or FDA at 1-800-FDA-1088 or www.fda.gov/medwatch.

8 USE IN SPECIFIC POPULATIONS

- Lactation: Advise not to breastfeed. (8.2)

FULL PRESCRIBING INFORMATION

1 INDICATIONS AND USAGE

1.1 Unresectable or Metastatic Melanoma

OPDIVO, as a single agent or in combination with ipilimumab, is indicated for the treatment of adult and pediatric patients 12 years and older with unresectable or metastatic melanoma.

1.2 Adjuvant Treatment of Melanoma

OPDIVO is indicated for the adjuvant treatment of adult and pediatric patients 12 years and older with completely resected Stage IIB, Stage IIC, Stage III, or Stage IV melanoma.

1.3 Neoadjuvant Treatment of Resectable Non-Small Cell Lung Cancer

OPDIVO, in combination with platinum-doublet chemotherapy, is indicated as neoadjuvant treatment of adult patients with resectable (tumors ≥4 cm or node positive) non-small cell lung cancer (NSCLC).

1.4 Neoadjuvant and Adjuvant Treatment of Resectable Non-Small Cell Lung Cancer

OPDIVO, in combination with platinum-doublet chemotherapy, is indicated for the neoadjuvant treatment of adult patients with resectable (tumors ≥4 cm or node positive) NSCLC and no known epidermal growth factor receptor (EGFR) mutations or anaplastic lymphoma kinase (ALK) rearrangements, followed by single-agent OPDIVO as adjuvant treatment after surgery.

1.5 Metastatic Non-Small Cell Lung Cancer

- OPDIVO, in combination with ipilimumab, is indicated for the first-line treatment of adult patients with metastatic NSCLC whose tumors express PD-L1 (≥1%) as determined by an FDA-approved test [see Dosage and Administration (2.1)], with no EGFR or ALK genomic tumor aberrations.
- OPDIVO, in combination with ipilimumab and 2 cycles of platinum-doublet chemotherapy, is indicated for the first-line treatment of adult patients with metastatic or recurrent NSCLC, with no EGFR or ALK genomic tumor aberrations.
- OPDIVO is indicated for the treatment of adult patients with metastatic NSCLC with progression on or after platinum-based chemotherapy. Patients with EGFR or ALK genomic tumor aberrations should have disease progression on FDA-approved therapy for these aberrations prior to receiving OPDIVO.

1.6 Malignant Pleural Mesothelioma

OPDIVO, in combination with ipilimumab, is indicated for the first-line treatment of adult patients with unresectable malignant pleural mesothelioma.

1.7 Advanced Renal Cell Carcinoma

- OPDIVO, in combination with ipilimumab, is indicated for the first-line treatment of adult patients with intermediate or poor risk advanced RCC.
- OPDIVO, in combination with cabozantinib, is indicated for the first-line treatment of adult patients with advanced RCC.
- OPDIVO, as a single agent, is indicated for the treatment of adult patients with advanced renal cell carcinoma (RCC) who have received prior anti-angiogenic therapy.

1.8 Classical Hodgkin Lymphoma

OPDIVO is indicated for the treatment of adult patients with classical Hodgkin lymphoma (cHL) that has relapsed or progressed after:

- autologous hematopoietic stem cell transplantation (HSCT) and brentuximab vedotin, or
- 3 or more lines of systemic therapy that includes autologous HSCT.

This indication is approved under accelerated approval based on overall response rate [see Clinical Studies (14.8)]. Continued approval for this indication may be contingent upon verification and description of clinical benefit in confirmatory trials.

1.9 Squamous Cell Carcinoma of the Head and Neck

OPDIVO is indicated for the treatment of adult patients with recurrent or metastatic squamous cell carcinoma of the head and neck (SCCHN) with disease progression on or after platinum-based therapy.

1.10 Urothelial Carcinoma

OPDIVO is indicated for the adjuvant treatment of adult patients with urothelial carcinoma (UC) who are at high risk of recurrence after undergoing radical resection of UC [see Clinical Studies (14.10)].

OPDIVO, in combination with cisplatin and gemcitabine, is indicated for the first-line treatment of adult patients with unresectable or metastatic urothelial carcinoma.

OPDIVO is indicated for the treatment of adult patients with locally advanced or metastatic urothelial carcinoma who:

- have disease progression during or following platinum-containing chemotherapy.
- have disease progression within 12 months of neoadjuvant or adjuvant treatment with platinum-containing chemotherapy.

1.11 Microsatellite Instability-High or Mismatch Repair Deficient Metastatic Colorectal Cancer

- OPDIVO, in combination with ipilimumab, is indicated for the treatment of adult and pediatric patients 12 years and older with unresectable or metastatic microsatellite instability-high (MSI-H) or mismatch repair deficient (dMMR) colorectal cancer (CRC).
- OPDIVO, as a single agent, is indicated for the treatment of adult and pediatric patients 12 years and older with microsatellite instability-high (MSI-H) or mismatch repair deficient (dMMR) metastatic colorectal cancer (CRC) that has progressed following treatment with a fluoropyrimidine, oxaliplatin, and irinotecan.

1.12 Hepatocellular Carcinoma

- OPDIVO, in combination with ipilimumab, is indicated for the first-line treatment of adult patients with unresectable or metastatic hepatocellular carcinoma (HCC).
- OPDIVO, in combination with ipilimumab, is indicated for the treatment of adult patients with unresectable or metastatic HCC who have been previously treated with sorafenib.

1.13 Esophageal Cancer

- OPDIVO is indicated for the adjuvant treatment of completely resected esophageal or gastroesophageal junction cancer with residual pathologic disease in adult patients who have received neoadjuvant chemoradiotherapy (CRT).
- OPDIVO, in combination with fluoropyrimidine- and platinum-containing chemotherapy, is indicated for the first-line treatment of adult patients with unresectable advanced or metastatic esophageal squamous cell carcinoma (ESCC) whose tumors express PD-L1 (≥1) [see Dosage and Administration (2.1)].
- OPDIVO, in combination with ipilimumab, is indicated for the first-line treatment of adult patients with unresectable advanced or metastatic esophageal squamous cell carcinoma (ESCC) whose tumors express PD-L1 (≥1) [see Dosage and Administration (2.1)].
- OPDIVO is indicated for the treatment of adult patients with unresectable advanced, recurrent or metastatic esophageal squamous cell carcinoma (ESCC) after prior fluoropyrimidine- and platinum-based chemotherapy.

1.14 Gastric Cancer, Gastroesophageal Junction Cancer, and Esophageal Adenocarcinoma

OPDIVO, in combination with fluoropyrimidine- and platinum-containing chemotherapy, is indicated for the treatment of adult patients with advanced or metastatic gastric cancer, gastroesophageal junction cancer, and esophageal adenocarcinoma whose tumors express PD-L1 (≥1) [see Dosage and Administration (2.1)].

2 DOSAGE AND ADMINISTRATION

2.1 Patient Selection

Information on FDA-approved tests for patient selection is available at:

https://www.fda.gov/CompanionDiagnostics

Non-Small Cell Lung Cancer

- Select patients with metastatic NSCLC for treatment with OPDIVO in combination with ipilimumab based on PD-L1 expression [see Clinical Studies (14.5)].

Esophageal Cancer

- Select patients with unresectable advanced or metastatic ESCC for treatment with OPDIVO in combination with fluoropyrimidine- and platinum-containing chemotherapy based on PD-L1 expression [see Clinical Studies (14.13)].
- Select patients with unresectable advanced or metastatic ESCC for treatment with OPDIVO in combination with ipilimumab based on PD-L1 expression [see Clinical Studies (14.13)].
  - An FDA-approved companion diagnostic for the detection of PD-L1 expression in patients with advanced or metastatic ESCC is not available.

Gastric Cancer, Gastroesophageal Junction Cancer, and Esophageal Adenocarcinoma

- Select patients with advanced or metastatic gastric cancer, gastroesophageal junction cancer, and esophageal adenocarcinoma for treatment with OPDIVO in combination with fluoropyrimidine- and platinum-containing chemotherapy based on PD-L1 expression [see Clinical Studies (14.14)].
  - An FDA-approved companion diagnostic for the detection of PD-L1 expression in patients with advanced or metastatic gastric cancer, gastroesophageal junction cancer, and esophageal adenocarcinoma is not available.

2.2 Recommended Dosage

The recommended dosages of intravenous OPDIVO as a single agent are presented in Table 1.

Administer OPDIVO as a 30-minute intravenous infusion [see Dosage and Administration (2.4)].

Table 1: Recommended Dosages for Intravenous OPDIVO as a Single Agent
Indication | Recommended OPDIVO Dosage | Duration of Therapy
Metastatic non-small cell lung cancer | 240 mg every 2 weeks; or; 480 mg every 4 weeks | Until disease progression or unacceptable toxicity
Advanced renal cell carcinoma | 240 mg every 2 weeks; or; 480 mg every 4 weeks | Until disease progression or unacceptable toxicity
Classical Hodgkin lymphoma | 240 mg every 2 weeks; or; 480 mg every 4 weeks | Until disease progression or unacceptable toxicity
Squamous cell carcinoma of the head and neck | 240 mg every 2 weeks; or; 480 mg every 4 weeks | Until disease progression or unacceptable toxicity
Locally advanced or metastatic urothelial carcinoma | 240 mg every 2 weeks; or; 480 mg every 4 weeks | Until disease progression or unacceptable toxicity
Esophageal squamous cell carcinoma | 240 mg every 2 weeks; or; 480 mg every 4 weeks | Until disease progression or unacceptable toxicity
Unresectable or metastatic melanoma | Adult patients and pediatric patients age 12 years and older and weighing 40 kg or more:; 240 mg every 2 weeks; or; 480 mg every 4 weeks | Until disease progression or unacceptable toxicity
Unresectable or metastatic melanoma | Pediatric patients age 12 years and older and weighing less than 40 kg:; 3 mg/kg every 2 weeks; or; 6 mg/kg every 4 weeks | Until disease progression or unacceptable toxicity
Adjuvant treatment of melanoma | Adult patients and pediatric patients age 12 years and older and weighing 40 kg or more:; 240 mg every 2 weeks; or; 480 mg every 4 weeks | Until disease recurrence or unacceptable toxicity for up to 1 year
Adjuvant treatment of melanoma | Pediatric patients age 12 years and older and weighing less than 40 kg:; 3 mg/kg every 2 weeks; or; 6 mg/kg every 4 weeks | Until disease recurrence or unacceptable toxicity for up to 1 year
Adjuvant treatment of urothelial carcinoma (UC) | 240 mg every 2 weeks; or; 480 mg every 4 weeks | Until disease recurrence or unacceptable toxicity for up to 1 year
Microsatellite instability-high (MSI-H) or mismatch repair deficient (dMMR) metastatic colorectal cancer that has progressed following prior treatment for metastatic disease | Adult patients and pediatric patients age 12 years and older and weighing 40 kg or more:; 240 mg every 2 weeks; or; 480 mg every 4 weeks | Until disease progression or unacceptable toxicity
Microsatellite instability-high (MSI-H) or mismatch repair deficient (dMMR) metastatic colorectal cancer that has progressed following prior treatment for metastatic disease | Pediatric patients age 12 years and older and weighing less than 40 kg:; 3 mg/kg every 2 weeks | Until disease progression or unacceptable toxicity
Adjuvant treatment of resected esophageal or gastroesophageal junction cancer | 240 mg every 2 weeks; or; 480 mg every 4 weeks | Until disease progression or unacceptable toxicity for a total treatment duration of 1 year

The recommended dosages of OPDIVO in combination with other therapeutic agents are presented in Table 2. Administer OPDIVO on the same day as other therapeutic agents.

Refer to the respective Prescribing Information for each therapeutic agent administered in combination with OPDIVO for the recommended dosage information, as appropriate.

Table 2: Recommended Dosages of Intravenous OPDIVO in Combination with Other Therapeutic Agents
Indication | Recommended OPDIVO Dosage | Duration of Therapy
Unresectable or metastatic melanoma | 1 mg/kg every 3 weeks with ipilimumab 3 mg/kg | In combination with ipilimumab for a maximum of 4 doses or until unacceptable toxicity, whichever occurs earlier
Unresectable or metastatic melanoma | Adult patients and pediatric patients age 12 years and older and weighing 40 kg or more:; 240 mg every 2 weeks or 480 mg every 4 weeks | After completing 4 doses of combination therapy, administer as single agent until disease progression or unacceptable toxicity
Unresectable or metastatic melanoma | Pediatric patients age 12 years and older and weighing less than 40 kg:; 3 mg/kg every 2 weeks or 6 mg/kg every 4 weeks | After completing 4 doses of combination therapy, administer as single agent until disease progression or unacceptable toxicity
Neoadjuvant treatment of resectable non-small cell lung cancer | 360 mg every 3 weeks with platinum-doublet chemotherapy on the same day every 3 weeks | In combination with platinum-doublet chemotherapy for 3 cycles
Neoadjuvant and adjuvant treatment of resectable non-small cell lung cancer | Neoadjuvant: 360 mg every 3 weeks with platinum-doublet chemotherapy on the same day every 3 weeks | Neoadjuvant treatment in combination with chemotherapy for up to 4 cycles or until disease progression or unacceptable toxicity, followed by adjuvant treatment with OPDIVO as a single agent after surgery for up to 13 cycles (approximately 1 year) or until disease recurrence or unacceptable toxicity
Neoadjuvant and adjuvant treatment of resectable non-small cell lung cancer | Adjuvant: 480 mg every 4 weeks | Neoadjuvant treatment in combination with chemotherapy for up to 4 cycles or until disease progression or unacceptable toxicity, followed by adjuvant treatment with OPDIVO as a single agent after surgery for up to 13 cycles (approximately 1 year) or until disease recurrence or unacceptable toxicity
Metastatic non-small cell lung cancer expressing PD‑L1 | 360 mg every 3 weeks with ipilimumab 1 mg/kg every 6 weeks | In combination with ipilimumab until disease progression, unacceptable toxicity, or up to 2 years in patients without disease progression
Metastatic or recurrent non-small cell lung cancer | 360 mg every 3 weeks with ipilimumab 1 mg/kg every 6 weeks and histology-based platinum‑doublet chemotherapy every 3 weeks | In combination with ipilimumab until disease progression, unacceptable toxicity, or up to 2 years in patients without disease progression
Metastatic or recurrent non-small cell lung cancer | 360 mg every 3 weeks with ipilimumab 1 mg/kg every 6 weeks and histology-based platinum‑doublet chemotherapy every 3 weeks | 2 cycles of histology-based platinum‑doublet chemotherapy
Malignant pleural mesothelioma | 360 mg every 3 weeks with ipilimumab 1 mg/kg every 6 weeks | In combination with ipilimumab until disease progression, unacceptable toxicity, or up to 2 years in patients without disease progression
Advanced renal cell carcinoma | 3 mg/kg every 3 weeks with ipilimumab 1 mg/kg | In combination with ipilimumab for 4 doses
Advanced renal cell carcinoma | 240 mg every 2 weeks or 480 mg every 4 weeks | After completing 4 doses of combination therapy with ipilimumab, administer as single agent until disease progression or unacceptable toxicity
Advanced renal cell carcinoma | 240 mg every 2 weeks or 480 mg every 4 weeks; Administer OPDIVO in combination with cabozantinib 40 mg orally once daily without food | OPDIVO: Until disease progression, unacceptable toxicity, or up to 2 years
Advanced renal cell carcinoma | 240 mg every 2 weeks or 480 mg every 4 weeks; Administer OPDIVO in combination with cabozantinib 40 mg orally once daily without food | Cabozantinib: Until disease progression or unacceptable toxicity
First-line unresectable or metastatic urothelial carcinoma | 360 mg every 3 weeks Administer OPDIVO in combination with cisplatin and gemcitabine on the same day every 3 weeks | In combination with cisplatin and gemcitabine for up to 6 cycles
First-line unresectable or metastatic urothelial carcinoma | 240 mg every 2 weeks or 480 mg every 4 weeks | After completing up to 6 cycles of combination therapy, administer as single agent until disease progression, unacceptable toxicity, or up to 2 years from first dose
Microsatellite instability-high (MSI‑H) or mismatch repair deficient (dMMR) metastatic colorectal cancer | Adult patients and pediatric patients age 12 years and older and weighing 40 kg or more:; 240 mg every 3 weeks with ipilimumab 1 mg/kg | In combination with ipilimumab; for a maximum of 4 doses
Microsatellite instability-high (MSI‑H) or mismatch repair deficient (dMMR) metastatic colorectal cancer | Pediatric patients age 12 years and older and weighing less than 40 kg: 3 mg/kg every 3 weeks with ipilimumab 1 mg/kg | In combination with ipilimumab; for a maximum of 4 doses
Microsatellite instability-high (MSI‑H) or mismatch repair deficient (dMMR) metastatic colorectal cancer | Adult patients and pediatric patients age 12 years and older and weighing 40 kg or more:; 240 mg every 2 weeks or 480 mg every 4 weeks | After completing a maximum of 4 doses of combination therapy, administer as single agent until disease progression or unacceptable toxicity, or up to 2 years
Microsatellite instability-high (MSI‑H) or mismatch repair deficient (dMMR) metastatic colorectal cancer | Pediatric patients age 12 years and older and weighing less than 40 kg:; 3 mg/kg every 2 weeks or 6 mg/kg every 4 weeks | After completing a maximum of 4 doses of combination therapy, administer as single agent until disease progression or unacceptable toxicity, or up to 2 years
Hepatocellular carcinoma | 1 mg/kg every 3 weeks with ipilimumab 3 mg/kg | In combination with ipilimumab for a maximum of 4 doses
Hepatocellular carcinoma | 240 mg every 2 weeks or 480 mg every 4 weeks | After completing a maximum of 4 doses of combination therapy, administer as single agent until disease progression, unacceptable toxicity, or up to 2 years
Esophageal squamous cell carcinoma | 240 mg every 2 weeks or 480 mg every 4 weeks; Administer OPDIVO in combination with fluoropyrimidine- and platinum‑containing chemotherapy | OPDIVO: Until disease progression, unacceptable toxicity, or up to 2 years
Esophageal squamous cell carcinoma | 240 mg every 2 weeks or 480 mg every 4 weeks; Administer OPDIVO in combination with fluoropyrimidine- and platinum‑containing chemotherapy | Chemotherapy: Until disease progression or unacceptable toxicity
Esophageal squamous cell carcinoma | 3 mg/kg every 2 weeks or 360 mg every 3 weeks with ipilimumab 1 mg/kg every 6 weeks | In combination with ipilimumab until disease progression, unacceptable toxicity, or up to 2 years
Gastric cancer, Gastroesophageal junction cancer, and Esophageal adenocarcinoma | 240 mg every 2 weeks with fluoropyrimidine- and platinum‑containing chemotherapy every 2 weeks or 360 mg every 3 weeks with fluoropyrimidine- and platinum‑containing chemotherapy every 3 weeks | Until disease progression, unacceptable toxicity, or up to 2 years

2.3 Dosage Modifications

No dose reduction for OPDIVO is recommended. In general, withhold OPDIVO for severe (Grade 3) immune-mediated adverse reactions. Permanently discontinue OPDIVO for life-threatening (Grade 4) immune-mediated adverse reactions, recurrent severe (Grade 3) immune-mediated reactions that require systemic immunosuppressive treatment, or an inability to reduce corticosteroid dose to 10 mg or less of prednisone or equivalent per day within 12 weeks of initiating steroids.

Dosage modifications for OPDIVO or OPDIVO in combination for adverse reactions that require management different from these general guidelines are summarized in Table 3 and Table 4.

When OPDIVO is administered in combination with ipilimumab, withhold or permanently discontinue both ipilimumab and OPDIVO for an adverse reaction meeting these dose modification guidelines.

Table 3: Recommended Dosage Modifications for Adverse Reactions
Adverse Reaction | Severity | Dosage Modification
Immune-Mediated Adverse Reactions [see Warnings and Precautions (5.1)]
Pneumonitis | Grade 2 | Withholda
Pneumonitis | Grades 3 or 4 | Permanently discontinue
Colitis; For colitis in patients treated with combination therapy with ipilimumab, see Table 4. | Grade 2 or 3 | Withholda
Colitis; For colitis in patients treated with combination therapy with ipilimumab, see Table 4. | Grade 4 | Permanently discontinue
Hepatitis with no tumor involvement of the liver; For liver enzyme elevations in patients treated with combination therapy with ipilimumab, see Table 4. | AST/ALT increases to >3 and ≤8 times ULN; or; Total bilirubin increases to >1.5 and ≤3 times ULN. | Withholda
Hepatitis with no tumor involvement of the liver; For liver enzyme elevations in patients treated with combination therapy with ipilimumab, see Table 4. | AST or ALT increases to >8 times ULN; or; Total bilirubin increases to >3 times ULN. | Permanently discontinue
Hepatitis with tumor involvement of the liverb; For liver enzyme elevations in patients treated with combination therapy with ipilimumab, see Table 4. | Baseline AST/ALT is >1 and ≤3 times ULN and increases to >5 and ≤10 times ULN; or; Baseline AST/ALT is >3 and ≤5 times ULN and increases to >8 and ≤10 times ULN. | Withholda
Hepatitis with tumor involvement of the liverb; For liver enzyme elevations in patients treated with combination therapy with ipilimumab, see Table 4. | AST/ALT increases to >10 times ULN; or; Total bilirubin increases to >3 times ULN. | Permanently discontinue
Endocrinopathiesc | Grade 3 or 4 | Withhold until clinically stable or permanently discontinue depending on severity
Nephritis with Renal Dysfunction | Grade 2 or 3 increased blood creatinine | Withholda
Nephritis with Renal Dysfunction | Grade 4 increased blood creatinine | Permanently discontinue
Exfoliative Dermatologic Conditions | Suspected SJS, TEN, or DRESS | Withhold
Exfoliative Dermatologic Conditions | Confirmed SJS, TEN, or DRESS | Permanently discontinue
Myocarditis | Grades 2, 3, or 4 | Permanently discontinue
Neurological Toxicities | Grade 2 | Withholda
Neurological Toxicities | Grade 3 or 4 | Permanently discontinue
Other Adverse Reactions
Infusion-Related Reactions; [see Warnings and Precautions (5.2)] | Grade 1 or 2 | Interrupt or slow the rate of infusion
Infusion-Related Reactions; [see Warnings and Precautions (5.2)] | Grade 3 or 4 | Permanently discontinue
a Resume in patients with complete or partial resolution (Grade 0 to 1) after corticosteroid taper. Permanently discontinue if no complete or partial resolution within 12 weeks of last dose or inability to reduce prednisone to 10 mg per day (or equivalent) or less within 12 weeks of initiating steroids.
b If AST and ALT are less than or equal to ULN at baseline, withhold or permanently discontinue OPDIVO based on recommendations for hepatitis with no liver involvement.
c Depending on clinical severity, consider withholding for Grade 2 endocrinopathy until symptom improvement with hormone replacement. Resume once acute symptoms have resolved.
ALT = alanine aminotransferase, AST = aspartate aminotransferase, DRESS = Drug Rash with Eosinophilia and Systemic Symptoms, SJS = Stevens Johnson Syndrome, TEN = toxic epidermal necrolysis, ULN = upper limit normal

Table 4: Recommended Dosage Modifications for Adverse Reactions in Patients Treated with Combination Therapy
Treatment | Adverse Reaction | Severity | Dosage Modification
OPDIVO in combination with ipilimumab | Colitis | Grade 2 | Withholda
OPDIVO in combination with ipilimumab | Colitis | Grade 3 or 4 | Permanently discontinue
OPDIVO in combination with ipilimumab | Hepatitis with no tumor involvement of the liver; or; Hepatitis with tumor involvement of the liver/non-HCC | AST/ALT increases to >3 times ULN and ≤5 times ULN; or; Total bilirubin increases to ≥1.5 and ≤3 times ULN. | Withholda
OPDIVO in combination with ipilimumab | Hepatitis with no tumor involvement of the liver; or; Hepatitis with tumor involvement of the liver/non-HCC | AST or ALT >5 times ULN; or; Total bilirubin >3 times ULN. | Permanently discontinue
OPDIVO in combination with ipilimumab | Hepatitis with tumor involvement of the liverb/HCC | Baseline AST/ALT is >1 and ≤3 times ULN and increases to >5 and ≤10 times ULN; or; Baseline AST/ALT is >3 and ≤5 times ULN and increases to >8 and ≤10 times ULN. | Withholda
OPDIVO in combination with ipilimumab | Hepatitis with tumor involvement of the liverb/HCC | AST/ALT increases to >10 times ULN; or; Total bilirubin increases to >3 times ULN. | Permanently discontinue
OPDIVO in combination with cabozantinib | Liver enzyme elevations | ALT or AST >3 times ULN but ≤10 times ULN with concurrent total bilirubin <2 times ULN | Withholdc both OPDIVO and cabozantinib until adverse reactions recoverd to Grades 0‑1
OPDIVO in combination with cabozantinib | Liver enzyme elevations | ALT or AST >10 times ULN; or >3 times ULN with concurrent total bilirubin ≥2 times ULN | Permanently discontinuec both OPDIVO and cabozantinib
a Resume in patients with complete or partial resolution (Grade 0 to 1) after corticosteroid taper. Permanently discontinue if no complete or partial resolution within 12 weeks of last dose or inability to reduce prednisone to 10 mg per day (or equivalent) or less within 12 weeks of initiating steroids.
b If AST and ALT are less than or equal to ULN at baseline, withhold or permanently discontinue OPDIVO in combination with ipilimumab based on recommendations for hepatitis with no liver involvement.
c Consider corticosteroid therapy for hepatic adverse reactions if OPDIVO is withheld or discontinued when administered in combination with cabozantinib.
d After recovery, rechallenge with one or both of OPDIVO and cabozantinib may be considered. If rechallenging with cabozantinib with or without OPDIVO, refer to cabozantinib Prescribing Information.

2.4 Preparation and Administration

Visually inspect for particulate matter and discoloration. OPDIVO is a clear to opalescent, colorless to pale-yellow solution. Discard if cloudy, discolored, or contains extraneous particulate matter other than a few translucent-to-white, proteinaceous particles. Do not shake.

Preparation

- Withdraw the required volume of OPDIVO and transfer into an intravenous container.
- Dilute OPDIVO with either 0.9% Sodium Chloride Injection, USP or 5% Dextrose Injection, USP to prepare an infusion with a final concentration ranging from 1 mg/mL to 10 mg/mL. The total volume of infusion must not exceed 160 mL.
  - For adult and pediatric patients with body weight 40 kg or greater, do not exceed a total volume of infusion of 160 mL.
  - For adult and pediatric patients with body weight less than 40 kg, do not exceed a total volume of infusion of 4 mL/kg of body weight.
- Mix diluted solution by gentle inversion. Do not shake.
- Discard partially used vials or empty vials of OPDIVO.
- The product does not contain a preservative.
- After preparation, store the diluted solution either:
  - at room temperature at 20°C to 25°C (68°F to 77°F) and room light for no more than 8 hours from the time of preparation to end of the infusion. Discard diluted solution if not used within 8 hours from the time of preparation; or
  - under refrigeration at 2°C to 8°C (36°F to 46°F) and protected from light for no more than 7 days from the time of preparation to end of infusion. Discard diluted solution if not used within 7 days from the time of preparation.
- Do not freeze.

Administration

- Administer the infusion, after dilution, over 30 minutes through an intravenous line containing a sterile, nonpyrogenic, low protein binding in-line filter (pore size of 0.2 micrometer to 1.2 micrometer).
- Administer OPDIVO in combination with other therapeutic agents as follows:

Combination Therapy
Ipilimumab | Administer OPDIVO first, followed by the other therapeutic agent(s).
Platinum-Doublet Chemotherapy | Administer OPDIVO first, followed by the other therapeutic agent(s).
Ipilimumab and Platinum-Doublet Chemotherapy | Administer OPDIVO first, followed by the other therapeutic agent(s).
Fluoropyrimidine- and Platinum- Containing Chemotherapy | Administer OPDIVO first, followed by the other therapeutic agent(s).

- Use separate infusion bags and filters for each infusion.
- Flush the intravenous line at end of infusion.
- Do not co-administer other drugs through the same intravenous line.

3 DOSAGE FORMS AND STRENGTHS

Injection: 40 mg/4 mL (10 mg/mL), 100 mg/10 mL (10 mg/mL), 120 mg/12 mL (10 mg/mL), and 240 mg/24 mL (10 mg/mL) clear to opalescent, colorless to pale-yellow solution in a single-dose vial.

4 CONTRAINDICATIONS

None.

5 WARNINGS AND PRECAUTIONS

5.1 Severe and Fatal Immune-Mediated Adverse Reactions

OPDIVO is a monoclonal antibody that belongs to a class of drugs that bind to either the programmed death-receptor 1 (PD-1) or the PD-ligand 1 (PD-L1), blocking the PD-1/PD-L1 pathway, thereby removing inhibition of the immune response, potentially breaking peripheral tolerance and inducing immune-mediated adverse reactions. Important immune-mediated adverse reactions listed under Warnings and Precautions may not include all possible severe and fatal immune-mediated reactions.

Immune-mediated adverse reactions, which may be severe or fatal, can occur in any organ system or tissue. Immune-mediated adverse reactions can occur at any time after starting treatment with a PD-1/PD-L1 blocking antibody. While immune-mediated adverse reactions usually manifest during treatment with PD‑1/PD-L1 blocking antibodies, immune-mediated adverse reactions can also manifest after discontinuation of PD-1/PD-L1 blocking antibodies.

Early identification and management of immune-mediated adverse reactions are essential to ensure safe use of PD-1/PD-L1 blocking antibodies. Monitor patients closely for symptoms and signs that may be clinical manifestations of underlying immune-mediated adverse reactions. Evaluate liver enzymes, creatinine, and thyroid function at baseline and periodically during treatment. In cases of suspected immune-mediated adverse reactions, initiate appropriate workup to exclude alternative etiologies, including infection. Institute medical management promptly, including specialty consultation as appropriate.

Withhold or permanently discontinue OPDIVO depending on severity [see Dosage and Administration (2.3)]. In general, if OPDIVO requires interruption or discontinuation, administer systemic corticosteroid therapy (1 to 2 mg/kg/day prednisone or equivalent) until improvement to Grade 1 or less. Upon improvement to Grade 1 or less, initiate corticosteroid taper and continue to taper over at least 1 month. Consider administration of other systemic immunosuppressants in patients whose immune-mediated adverse reactions are not controlled with corticosteroid therapy.

Toxicity management guidelines for adverse reactions that do not necessarily require systemic steroids (e.g., endocrinopathies and dermatologic reactions) are discussed below.

Immune-Mediated Pneumonitis

OPDIVO can cause immune-mediated pneumonitis, which is defined as requiring use of steroids and no clear alternate etiology. In patients treated with other PD-1/PD-L1 blocking antibodies, the incidence of pneumonitis is higher in patients who have received prior thoracic radiation.

OPDIVO as a Single Agent

Immune-mediated pneumonitis occurred in 3.1% (61/1994) of patients receiving OPDIVO as a single agent, including Grade 4 (<0.1%), Grade 3 (0.9%), and Grade 2 (2.1%) adverse reactions. Pneumonitis led to permanent discontinuation of OPDIVO in 1.1% and withholding of OPDIVO in 0.8% of patients.

Systemic corticosteroids were required in 100% (61/61) of patients with pneumonitis. Pneumonitis resolved in 84% of the 61 patients. Of the 15 patients in whom OPDIVO was withheld for pneumonitis, 14 reinitiated OPDIVO after symptom improvement; of these, 4 (29%) had recurrence of pneumonitis.

OPDIVO with Ipilimumab

OPDIVO 3 mg/kg with Ipilimumab 1 mg/kg: In NSCLC, immune-mediated pneumonitis occurred in 9% (50/576) of patients receiving OPDIVO 3 mg/kg every 2 weeks with ipilimumab 1 mg/kg every 6 weeks, including Grade 4 (0.5%), Grade 3 (3.5%), and Grade 2 (4%) immune-mediated pneumonitis. Four patients (0.7%) died due to pneumonitis. Immune-mediated pneumonitis led to permanent discontinuation of OPDIVO with ipilimumab in 5% of patients and withholding of OPDIVO with ipilimumab in 3.6% of patients.

Systemic corticosteroids were required in 100% of patients with pneumonitis. Pneumonitis resolved in 72% of the patients. Approximately 13% (2/16) of patients had recurrence of pneumonitis after reinitiation of OPDIVO with ipilimumab.

Immune-Mediated Colitis

OPDIVO can cause immune-mediated colitis, defined as requiring use of corticosteroids and no clear alternate etiology. A common symptom included in the definition of colitis was diarrhea. Cytomegalovirus (CMV) infection/reactivation has been reported in patients with corticosteroid-refractory immune-mediated colitis. In cases of corticosteroid-refractory colitis, consider repeating infectious workup to exclude alternative etiologies.

OPDIVO as a Single Agent

Immune-mediated colitis occurred in 2.9% (58/1994) of patients receiving OPDIVO as a single agent, including Grade 3 (1.7%) and Grade 2 (1%) adverse reactions. Colitis led to permanent discontinuation of OPDIVO in 0.7% and withholding of OPDIVO in 0.9% of patients.

Systemic corticosteroids were required in 100% (58/58) of patients with colitis. Four patients required addition of infliximab to high-dose corticosteroids. Colitis resolved in 86% of the 58 patients. Of the 18 patients in whom OPDIVO was withheld for colitis, 16 reinitiated OPDIVO after symptom improvement; of these, 12 (75%) had recurrence of colitis.

OPDIVO with Ipilimumab

OPDIVO 1 mg/kg with Ipilimumab 3 mg/kg: Immune-mediated colitis occurred in 25% (115/456) of patients with melanoma or HCC receiving OPDIVO 1 mg/kg with ipilimumab 3 mg/kg every 3 weeks, including Grade 4 (0.4%), Grade 3 (14%), and Grade 2 (8%) adverse reactions. Colitis led to permanent discontinuation of OPDIVO with ipilimumab in 14% and withholding of OPDIVO with ipilimumab in 4.4% of patients.

Systemic corticosteroids were required in 100% (115/115) of patients with colitis. Approximately 23% of patients required addition of infliximab to high-dose corticosteroids. Colitis resolved in 93% of the 115 patients. Of the 20 patients in whom OPDIVO with ipilimumab was withheld for colitis, 16 reinitiated treatment after symptom improvement; of these, 9 (56%) had recurrence of colitis.

OPDIVO 3 mg/kg with Ipilimumab 1 mg/kg: Immune-mediated colitis occurred in 9% (60/666) of patients with RCC or CRC receiving OPDIVO 3 mg/kg with ipilimumab 1 mg/kg every 3 weeks, including Grade 3 (4.4%) and Grade 2 (3.7%) adverse reactions. Colitis led to permanent discontinuation of OPDIVO with ipilimumab in 3.2% and withholding of OPDIVO with ipilimumab in 2.7% of patients with RCC or CRC.

Systemic corticosteroids were required in 100% (60/60) of patients with colitis. Approximately 23% of patients with immune-mediated colitis required addition of infliximab to high-dose corticosteroids. Colitis resolved in 95% of the 60 patients. Of the 18 patients in whom OPDIVO with ipilimumab was withheld for colitis, 16 reinitiated treatment after symptom improvement; of these, 10 (63%) had recurrence of colitis.

Immune-Mediated Hepatitis and Hepatotoxicity

OPDIVO can cause immune-mediated hepatitis, defined as requiring the use of corticosteroids and no clear alternate etiology.

OPDIVO as a Single Agent

Immune-mediated hepatitis occurred in 1.8% (35/1994) of patients receiving OPDIVO as a single agent, including Grade 4 (0.2%), Grade 3 (1.3%), and Grade 2 (0.4%) adverse reactions. Hepatitis led to permanent discontinuation of OPDIVO in 0.7% and withholding of OPDIVO in 0.6% of patients.

Systemic corticosteroids were required in 100% (35/35) of patients with hepatitis. Two patients required the addition of mycophenolic acid to high-dose corticosteroids. Hepatitis resolved in 91% of the 35 patients. Of the 12 patients in whom OPDIVO was withheld for hepatitis, 11 reinitiated OPDIVO after symptom improvement; of these, 9 (82%) had recurrence of hepatitis.

OPDIVO with Ipilimumab

OPDIVO 1 mg/kg with Ipilimumab 3 mg/kg: Immune-mediated hepatitis occurred in 15% (70/456) of patients with melanoma or HCC receiving OPDIVO 1 mg/kg with ipilimumab 3 mg/kg every 3 weeks, including Grade 4 (2.4%), Grade 3 (11%), and Grade 2 (1.8%) adverse reactions. Immune-mediated hepatitis led to permanent discontinuation of OPDIVO with ipilimumab in 8% or withholding of OPDIVO with ipilimumab in 3.5% of patients.

Systemic corticosteroids were required in 100% (70/70) of patients with hepatitis. Approximately 9% of patients with immune-mediated hepatitis required the addition of mycophenolic acid to high-dose corticosteroids. Hepatitis resolved in 91% of the 70 patients. Of the 16 patients in whom OPDIVO with ipilimumab was withheld for hepatitis, 14 reinitiated treatment after symptom improvement; of these, 8 (57%) had recurrence of hepatitis.

OPDIVO 3 mg/kg with Ipilimumab 1 mg/kg: Immune-mediated hepatitis occurred in 7% (48/666) of patients with RCC or CRC receiving OPDIVO 3 mg/kg with ipilimumab 1 mg/kg every 3 weeks, including Grade 4 (1.2%), Grade 3 (4.9%), and Grade 2 (0.4%) adverse reactions. Immune-mediated hepatitis led to permanent discontinuation of OPDIVO with ipilimumab in 3.6% and withholding of OPDIVO with ipilimumab in 2.6% of patients with RCC or CRC.

Systemic corticosteroids were required in 100% (48/48) of patients with hepatitis. Approximately 19% of patients with immune-mediated hepatitis required addition of mycophenolic acid to high-dose corticosteroids. Hepatitis resolved in 88% of the 48 patients. Of the 17 patients in whom OPDIVO with ipilimumab was withheld for hepatitis, 14 reinitiated treatment after symptom improvement; of these, 10 (71%) had recurrence of hepatitis.

OPDIVO with Cabozantinib

OPDIVO in combination with cabozantinib can cause hepatic toxicity with higher frequencies of Grade 3 and 4 ALT and AST elevations compared to OPDIVO alone. Monitor liver enzymes before initiation of and periodically throughout treatment. Consider more frequent monitoring of liver enzymes as compared to when the drugs are administered as single agents. For elevated liver enzymes, interrupt OPDIVO and cabozantinib and consider administering corticosteroids [see Dosage and Administration (2.3)].

With the combination of OPDIVO and cabozantinib, Grades 3 and 4 increased ALT or AST were seen in 11% of patients [see Adverse Reactions (6.1)]. ALT or AST >3 times ULN (Grade ≥2) was reported in 83 patients, of whom 23 (28%) received systemic corticosteroids; ALT or AST resolved to Grades 0-1 in 74 (89%). Among the 44 patients with Grade ≥2 increased ALT or AST who were rechallenged with either OPDIVO (n=11) or cabozantinib (n=9) administered as a single agent or with both (n=24), recurrence of Grade ≥2 increased ALT or AST was observed in 2 patients receiving OPDIVO, 2 patients receiving cabozantinib, and 7 patients receiving both OPDIVO and cabozantinib.

Immune-Mediated Endocrinopathies

Adrenal Insufficiency

OPDIVO can cause primary or secondary adrenal insufficiency. For grade 2 or higher adrenal insufficiency, initiate symptomatic treatment, including hormone replacement as clinically indicated. Withhold OPDIVO depending on severity [see Dosage and Administration (2.3)].

OPDIVO as a Single Agent

Adrenal insufficiency occurred in 1% (20/1994) of patients receiving OPDIVO as a single agent, including Grade 3 (0.4%) and Grade 2 (0.6%) adverse reactions. Adrenal insufficiency led to permanent discontinuation of OPDIVO in 0.1% and withholding of OPDIVO in 0.4% of patients.

Approximately 85% of patients with adrenal insufficiency received hormone replacement therapy. Systemic corticosteroids were required in 90% (18/20) of patients with adrenal insufficiency. Adrenal insufficiency resolved in 35% of the 20 patients. Of the 8 patients in whom OPDIVO was withheld for adrenal insufficiency, 4 reinitiated OPDIVO after symptom improvement and all required hormone replacement therapy for their ongoing adrenal insufficiency.

OPDIVO with Ipilimumab

OPDIVO 1 mg/kg with Ipilimumab 3 mg/kg: Adrenal insufficiency occurred in 8% (35/456) of patients with melanoma or HCC receiving OPDIVO 1 mg/kg with ipilimumab 3 mg/kg every 3 weeks, including Grade 4 (0.2%), Grade 3 (2.4%), and Grade 2 (4.2%) adverse reactions. Adrenal insufficiency led to permanent discontinuation of OPDIVO with ipilimumab in 0.4% and withholding of OPDIVO with ipilimumab in 2% of patients.

Approximately 71% (25/35) of patients with adrenal insufficiency received hormone replacement therapy, including systemic corticosteroids. Adrenal insufficiency resolved in 37% of the 35 patients. Of the 9 patients in whom OPDIVO with ipilimumab was withheld for adrenal insufficiency, 7 reinitiated treatment after symptom improvement and all required hormone replacement therapy for their ongoing adrenal insufficiency.

OPDIVO 3 mg/kg with Ipilimumab 1 mg/kg: Adrenal insufficiency occurred in 7% (48/666) of patients with RCC or CRC who received OPDIVO 3 mg/kg with ipilimumab 1 mg/kg every 3 weeks, including Grade 4 (0.3%), Grade 3 (2.5%), and Grade 2 (4.1%) adverse reactions. Adrenal insufficiency led to permanent discontinuation of OPDIVO with ipilimumab in 1.2% and withholding of OPDIVO with ipilimumab in 2.1% of patients with RCC or CRC.

Approximately 94% (45/48) of patients with adrenal insufficiency received hormone replacement therapy, including systemic corticosteroids. Adrenal insufficiency resolved in 29% of the 48 patients. Of the 14 patients in whom OPDIVO with ipilimumab was withheld for adrenal insufficiency, 11 reinitiated treatment after symptom improvement; of these, all received hormone replacement therapy and 2 (18%) had recurrence of adrenal insufficiency.

OPDIVO with Cabozantinib

Adrenal insufficiency occurred in 4.7% (15/320) of patients with RCC who received OPDIVO with cabozantinib, including Grade 3 (2.2%), and Grade 2 (1.9%) adverse reactions. Adrenal insufficiency led to permanent discontinuation of OPDIVO and cabozantinib in 0.9% and withholding of OPDIVO and cabozantinib in 2.8% of patients with RCC.

Approximately 80% (12/15) of patients with adrenal insufficiency received hormone replacement therapy, including systemic corticosteroids. Adrenal insufficiency resolved in 27% (n=4) of the 15 patients. Of the 9 patients in whom OPDIVO with cabozantinib was withheld for adrenal insufficiency, 6 reinstated treatment after symptom improvement; of these, all (n=6) received hormone replacement therapy and 2 had recurrence of adrenal insufficiency.

Hypophysitis

OPDIVO can cause immune-mediated hypophysitis. Hypophysitis can present with acute symptoms associated with mass effect such as headache, photophobia, or visual field defects. Hypophysitis can cause hypopituitarism. Initiate hormone replacement as clinically indicated. Withhold or permanently discontinue OPDIVO depending on severity [see Dosage and Administration (2.3)].

OPDIVO as a Single Agent

Hypophysitis occurred in 0.6% (12/1994) of patients receiving OPDIVO as a single agent, including Grade 3 (0.2%) and Grade 2 (0.3%) adverse reactions. Hypophysitis led to permanent discontinuation of OPDIVO in <0.1% and withholding of OPDIVO in 0.2% of patients.

Approximately 67% (8/12) of patients with hypophysitis received hormone replacement therapy, including systemic corticosteroids. Hypophysitis resolved in 42% of the 12 patients. Of the 3 patients in whom OPDIVO was withheld for hypophysitis, 2 reinitiated OPDIVO after symptom improvement; of these, none had recurrence of hypophysitis.

OPDIVO with Ipilimumab

OPDIVO 1 mg/kg with Ipilimumab 3 mg/kg: Hypophysitis occurred in 9% (42/456) of patients with melanoma or HCC receiving OPDIVO 1 mg/kg with ipilimumab 3 mg/kg every 3 weeks, including Grade 3 (2.4%) and Grade 2 (6%) adverse reactions. Hypophysitis led to permanent discontinuation of OPDIVO with ipilimumab in 0.9% and withholding of OPDIVO with ipilimumab in 4.2% of patients.

Approximately 86% of patients with hypophysitis received hormone replacement therapy. Systemic corticosteroids were required in 88% (37/42) of patients with hypophysitis. Hypophysitis resolved in 38% of the 42 patients. Of the 19 patients in whom OPDIVO with ipilimumab was withheld for hypophysitis, 9 reinitiated treatment after symptom improvement; of these, 1 (11%) had recurrence of hypophysitis.

OPDIVO 3 mg/kg with Ipilimumab 1 mg/kg: Hypophysitis occurred in 4.4% (29/666) of patients with RCC or CRC receiving OPDIVO 3 mg/kg with ipilimumab 1 mg/kg every 3 weeks, including Grade 4 (0.3%), Grade 3 (2.4%), and Grade 2 (0.9%) adverse reactions. Hypophysitis led to permanent discontinuation of OPDIVO with ipilimumab in 1.2% and withholding of OPDIVO with ipilimumab in 2.1% of patients with RCC or CRC.

Approximately 72% (21/29) of patients with hypophysitis received hormone replacement therapy, including systemic corticosteroids. Hypophysitis resolved in 59% of the 29 patients. Of the 14 patients in whom OPDIVO with ipilimumab was withheld for hypophysitis, 11 reinitiated treatment after symptom improvement; of these, 2 (18%) had recurrence of hypophysitis.

Thyroid Disorders

OPDIVO can cause immune-mediated thyroid disorders. Thyroiditis can present with or without endocrinopathy. Hypothyroidism can follow hyperthyroidism. Initiate hormone replacement or medical management as clinically indicated. Withhold or permanently discontinue OPDIVO depending on severity [see Dosage and Administration (2.3)].

Thyroiditis

OPDIVO as a Single Agent

Thyroiditis occurred in 0.6% (12/1994) of patients receiving OPDIVO as a single agent, including Grade 2 (0.2%) adverse reactions. Thyroiditis led to permanent discontinuation of OPDIVO in no patients and withholding of OPDIVO in 0.2% of patients.

Systemic corticosteroids were required in 17% (2/12) of patients with thyroiditis. Thyroiditis resolved in 58% of the 12 patients. Of the 3 patients in whom OPDIVO was withheld for thyroiditis, 1 reinitiated OPDIVO after symptom improvement without recurrence of thyroiditis.

Hyperthyroidism

OPDIVO as a Single Agent

Hyperthyroidism occurred in 2.7% (54/1994) of patients receiving OPDIVO as a single agent, including Grade 3 (<0.1%) and Grade 2 (1.2%) adverse reactions. Hyperthyroidism led to the permanent discontinuation of OPDIVO in no patients and withholding of OPDIVO in 0.4% of patients.

Approximately 19% of patients with hyperthyroidism received methimazole, 7% received carbimazole, and 4% received propylthiouracil. Systemic corticosteroids were required in 9% (5/54) of patients. Hyperthyroidism resolved in 76% of the 54 patients. Of the 7 patients in whom OPDIVO was withheld for hyperthyroidism, 4 reinitiated OPDIVO after symptom improvement; of these, none had recurrence of hyperthyroidism.

OPDIVO with Ipilimumab

OPDIVO 1 mg/kg with Ipilimumab 3 mg/kg: Hyperthyroidism occurred in 9% (42/456) of patients with melanoma or HCC who received OPDIVO 1 mg/kg with ipilimumab 3 mg/kg every 3 weeks, including Grade 3 (0.9%) and Grade 2 (4.2%) adverse reactions. Hyperthyroidism led to the permanent discontinuation of OPDIVO with ipilimumab in no patients and withholding of OPDIVO with ipilimumab in 2.4% of patients.

Approximately 26% of patients with hyperthyroidism received methimazole and 21% received carbimazole. Systemic corticosteroids were required in 17% (7/42) of patients. Hyperthyroidism resolved in 91% of the 42 patients. Of the 11 patients in whom OPDIVO with ipilimumab was withheld for hyperthyroidism, 8 reinitiated treatment after symptom improvement; of these, 1 (13%) had recurrence of hyperthyroidism.

OPDIVO 3 mg/kg with Ipilimumab 1 mg/kg: Hyperthyroidism occurred in 12% (80/666) of patients with RCC or CRC who received OPDIVO 3 mg/kg with ipilimumab 1 mg/kg every 3 weeks, including Grade 3 (0.6%) and Grade 2 (4.5%) adverse reactions. Hyperthyroidism led to permanent discontinuation of OPDIVO with ipilimumab in no patients and withholding of OPDIVO with ipilimumab in 2.3% of patients with RCC or CRC.

Of the 80 patients with RCC or CRC who developed hyperthyroidism, approximately 16% received methimazole and 3% received carbimazole. Systemic corticosteroids were required in 20% (16/80) of patients with hyperthyroidism. Hyperthyroidism resolved in 85% of the 80 patients. Of the 15 patients in whom OPDIVO with ipilimumab was withheld for hyperthyroidism, 11 reinitiated treatment after symptom improvement; of these, 3 (27%) had recurrence of hyperthyroidism.

Hypothyroidism

OPDIVO as a Single Agent

Hypothyroidism occurred in 8% (163/1994) of patients receiving OPDIVO as a single agent, including Grade 3 (0.2%) and Grade 2 (4.8%) adverse reactions. Hypothyroidism led to the permanent discontinuation of OPDIVO in no patients and withholding of OPDIVO in 0.5% of patients.

Approximately 79% of patients with hypothyroidism received levothyroxine. Systemic corticosteroids were required in 3.1% (5/163) of patients with hypothyroidism. Hypothyroidism resolved in 35% of the 163 patients. Of the 9 patients in whom OPDIVO was withheld for hypothyroidism, 3 reinitiated OPDIVO after symptom improvement; of these, 1 (33%) had recurrence of hypothyroidism.

OPDIVO with Ipilimumab

OPDIVO 1 mg/kg with Ipilimumab 3 mg/kg: Hypothyroidism occurred in 20% (91/456) of patients with melanoma or HCC receiving OPDIVO 1 mg/kg with ipilimumab 3 mg/kg every 3 weeks, including Grade 3 (0.4%) and Grade 2 (11%) adverse reactions. Hypothyroidism led to the permanent discontinuation of OPDIVO with ipilimumab in 0.9% and withholding of OPDIVO with ipilimumab in 0.9% of patients.

Approximately 89% of patients with hypothyroidism received levothyroxine. Systemic corticosteroids were required in 2.2% (2/91) of patients with hypothyroidism. Hypothyroidism resolved in 41% of the 91 patients. Of the 4 patients in whom OPDIVO with ipilimumab was withheld for hypothyroidism, 2 reinitiated treatment after symptom improvement; of these, none had recurrence of hypothyroidism.

OPDIVO 3 mg/kg with Ipilimumab 1 mg/kg: Hypothyroidism occurred in 18% (122/666) of patients with RCC or CRC who received OPDIVO 3 mg/kg and ipilimumab 1 mg/kg every 3 weeks, including Grade 3 (0.6%) and Grade 2 (11%) adverse reactions. Hypothyroidism led to permanent discontinuation of OPDIVO with ipilimumab in 0.2% and withholding of OPDIVO with ipilimumab in 1.4% of patients with RCC or CRC.

Of the 122 patients with RCC or CRC who developed hypothyroidism, approximately 82% received levothyroxine. Systemic corticosteroids were required in 7% (9/122) of patients with hypothyroidism. Hypothyroidism resolved in 27% of the 122 patients. Of the 9 patients in whom OPDIVO with ipilimumab was withheld for hypothyroidism, 5 reinitiated treatment after symptom improvement; of these, 1 (20%) had recurrence of hypothyroidism.

Type 1 Diabetes Mellitus, which can present with Diabetic Ketoacidosis

Monitor patients for hyperglycemia or other signs and symptoms of diabetes. Initiate treatment with insulin as clinically indicated. Withhold OPDIVO depending on severity [see Dosage and Administration (2.3)].

OPDIVO as a Single Agent

Diabetes occurred in 0.9% (17/1994) of patients receiving OPDIVO as a single agent, including Grade 3 (0.4%) and Grade 2 (0.3%) adverse reactions, and two cases of diabetic ketoacidosis. Diabetes led to the permanent discontinuation of OPDIVO in no patients and withholding of OPDIVO in 0.1% of patients.

No patients (0/17) with diabetes required systemic corticosteroids. Diabetes resolved in 29% of the 17 patients. Of the 2 patients in whom OPDIVO was withheld for diabetes, both reinitiated OPDIVO after symptom improvement; of these, neither had recurrence of diabetes.

Immune-Mediated Nephritis with Renal Dysfunction

OPDIVO can cause immune-mediated nephritis, which is defined as requiring use of steroids and no clear alternate etiology.

OPDIVO as a Single Agent

Immune-mediated nephritis and renal dysfunction occurred in 1.2% (23/1994) of patients receiving OPDIVO as a single agent, including Grade 4 (<0.1%), Grade 3 (0.5%), and Grade 2 (0.6%) adverse reactions. Immune-mediated nephritis and renal dysfunction led to permanent discontinuation of OPDIVO in 0.3% and withholding of OPDIVO in 0.4% of patients.

Systemic corticosteroids were required in 100% (23/23) of patients with nephritis and renal dysfunction. Nephritis and renal dysfunction resolved in 78% of the 23 patients. Of the 7 patients in whom OPDIVO was withheld for nephritis or renal dysfunction, 7 reinitiated OPDIVO after symptom improvement; of these, 1 (14%) had recurrence of nephritis or renal dysfunction.

Immune-Mediated Dermatologic Adverse Reactions

OPDIVO can cause immune-mediated rash or dermatitis, defined as requiring the use of steroids and no clear alternate etiology. Exfoliative dermatitis, including Stevens-Johnson Syndrome, toxic epidermal necrolysis (TEN), and DRESS (Drug Rash with Eosinophilia and Systemic Symptoms) has occurred with PD-1/PD-L1 blocking antibodies. Topical emollients and/or topical corticosteroids may be adequate to treat mild to moderate non-exfoliative rashes. Withhold or permanently discontinue OPDIVO depending on severity [see Dosage and Administration (2.3)].

OPDIVO as a Single Agent

Immune-mediated rash occurred in 9% (171/1994) of patients, including Grade 3 (1.1%) and Grade 2 (2.2%) adverse reactions. Immune-mediated rash led to permanent discontinuation of OPDIVO in 0.3% and withholding of OPDIVO in 0.5% of patients.

Systemic corticosteroids were required in 100% (171/171) of patients with immune-mediated rash. Rash resolved in 72% of the 171 patients. Of the 10 patients in whom OPDIVO was withheld for immune-mediated rash, 9 reinitiated OPDIVO after symptom improvement; of these, 3 (33%) had recurrence of immune-mediated rash.

OPDIVO with Ipilimumab

OPDIVO 1 mg/kg with Ipilimumab 3 mg/kg: Immune-mediated rash occurred in 28% (127/456) of patients with melanoma or HCC receiving OPDIVO 1 mg/kg with ipilimumab 3 mg/kg every 3 weeks, including Grade 3 (4.8%) and Grade 2 (10%) adverse reactions. Immune-mediated rash led to permanent discontinuation of OPDIVO with ipilimumab in 0.4% and withholding of OPDIVO with ipilimumab in 3.9% of patients.

Systemic corticosteroids were required in 100% (127/127) of patients with immune-mediated rash. Rash resolved in 84% of the 127 patients. Of the 18 patients in whom OPDIVO with ipilimumab was withheld for immune-mediated rash, 15 reinitiated treatment after symptom improvement; of these, 8 (53%) had recurrence of immune-mediated rash.

OPDIVO 3 mg/kg with Ipilimumab 1 mg/kg: Immune-mediated rash occurred in 16% (108/666) of patients with RCC or CRC who received OPDIVO 3 mg/kg with ipilimumab 1 mg/kg every 3 weeks, including Grade 3 (3.5%) and Grade 2 (4.2%) adverse reactions. Immune-mediated rash led to permanent discontinuation of OPDIVO with ipilimumab in 0.5% of patients and withholding of OPDIVO with ipilimumab in 2.0% of patients with RCC or CRC.

Systemic corticosteroids were required in 100% (108/108) of patients with immune-mediated rash. Rash resolved in 75% of the 108 patients. Of the 13 patients in whom OPDIVO with ipilimumab was withheld for immune-mediated rash, 11 reinitiated treatment after symptom improvement; of these, 5 (46%) had recurrence of immune-mediated rash.

Other Immune-Mediated Adverse Reactions

The following clinically significant immune-mediated adverse reactions occurred at an incidence of <1% (unless otherwise noted) in patients who received OPDIVO or OPDIVO in combination with ipilimumab, or were reported with the use of other PD-1/PD-L1 blocking antibodies. Severe or fatal cases have been reported for some of these adverse reactions.

Cardiac/Vascular: Myocarditis, pericarditis, vasculitis

Nervous System: Meningitis, encephalitis, myelitis and demyelination, myasthenic syndrome/myasthenia gravis (including exacerbation), Guillain-Barre syndrome, nerve paresis, autoimmune neuropathy

Ocular: Uveitis, iritis, and other ocular inflammatory toxicities can occur. Some cases can be associated with retinal detachment. Various grades of visual impairment, including blindness, can occur. If uveitis occurs in combination with other immune-mediated adverse reactions, consider a Vogt-Koyanagi-Harada-like syndrome, as this may require treatment with systemic steroids to reduce the risk of permanent vision loss

Gastrointestinal: Pancreatitis to include increases in serum amylase and lipase levels, gastritis, duodenitis

Musculoskeletal and Connective Tissue: Myositis/polymyositis, rhabdomyolysis, and associated sequelae including renal failure, arthritis, polymyalgia rheumatic

Endocrine: Hypoparathyroidism

Other (Hematologic/Immune): Hemolytic anemia, aplastic anemia, hemophagocytic lymphohistiocytosis, systemic inflammatory response syndrome, histiocytic necrotizing lymphadenitis (Kikuchi lymphadenitis), sarcoidosis, immune thrombocytopenic purpura, solid organ transplant rejection, other transplant (including corneal graft) rejection

5.2 Infusion-Related Reactions

OPDIVO can cause severe infusion-related reactions, which have been reported in <1% of patients in clinical trials. Discontinue OPDIVO in patients with severe or life-threatening infusion-related reactions. Interrupt or slow the rate of infusion in patients with mild or moderate infusion-related reactions [see Dosage and Administration (2.3)].

OPDIVO as a Single Agent

In patients who received OPDIVO as a 60-minute intravenous infusion, infusion-related reactions occurred in 6.4% (127/1994) of patients.

In a trial assessing the pharmacokinetics and safety of a more rapid infusion, in which patients received OPDIVO as a 60-minute intravenous infusion or a 30-minute intravenous infusion, infusion-related reactions occurred in 2.2% (8/368) and 2.7% (10/369) of patients, respectively. Additionally, 0.5% (2/368) and 1.4% (5/369) of patients, respectively, experienced adverse reactions within 48 hours of infusion that led to dose delay, permanent discontinuation, or withholding of OPDIVO.

OPDIVO with Ipilimumab

OPDIVO 1 mg/kg with Ipilimumab 3 mg/kg

Infusion-related reactions occurred in 2.5% (10/407) of patients with melanoma and in 8% (4/49) of patients with HCC who received OPDIVO 1 mg/kg with ipilimumab 3 mg/kg every 3 weeks.

OPDIVO 3 mg/kg with Ipilimumab 1 mg/kg

Infusion-related reactions occurred in 5.1% (28/547) of patients with RCC and 4.2% (5/119) of patients with CRC who received OPDIVO 3 mg/kg with ipilimumab 1 mg/kg every 3 weeks, respectively. Infusion-related reactions occurred in 12% (37/300) of patients with malignant pleural mesothelioma who received OPDIVO 3 mg/kg every 2 weeks with ipilimumab 1 mg/kg every 6 weeks.

5.3 Complications of Allogeneic Hematopoietic Stem Cell Transplantation

Fatal and other serious complications can occur in patients who receive allogeneic hematopoietic stem cell transplantation (HSCT) before or after being treated with a PD-1 receptor blocking antibody. Transplant-related complications include hyperacute graft-versus-host-disease (GVHD), acute GVHD, chronic GVHD, hepatic veno-occlusive disease (VOD) after reduced intensity conditioning, and steroid-requiring febrile syndrome (without an identified infectious cause) [see Adverse Reactions (6.1)]. These complications may occur despite intervening therapy between PD-1 blockade and allogeneic HSCT.

Follow patients closely for evidence of transplant-related complications and intervene promptly. Consider the benefit versus risks of treatment with a PD-1 receptor blocking antibody prior to or after an allogeneic HSCT.

5.4 Embryo-Fetal Toxicity

Based on its mechanism of action and data from animal studies, OPDIVO can cause fetal harm when administered to a pregnant woman. In animal reproduction studies, administration of nivolumab to cynomolgus monkeys from the onset of organogenesis through delivery resulted in increased abortion and premature infant death. Advise pregnant women of the potential risk to a fetus. Advise females of reproductive potential to use effective contraception during treatment with OPDIVO and for 5 months after the last dose [see Use in Specific Populations (8.1, 8.3)].

5.5 Increased Mortality in Patients with Multiple Myeloma when OPDIVO Is Added to a Thalidomide Analogue and Dexamethasone

In randomized clinical trials in patients with multiple myeloma, the addition of a PD-1 blocking antibody, including OPDIVO, to a thalidomide analogue plus dexamethasone, a use for which no PD-1 or PD-L1 blocking antibody is indicated, resulted in increased mortality. Treatment of patients with multiple myeloma with a PD-1 or PD-L1 blocking antibody in combination with a thalidomide analogue plus dexamethasone is not recommended outside of controlled clinical trials.

6 ADVERSE REACTIONS

The following clinically significant adverse reactions are described elsewhere in the labeling.

- Severe and Fatal Immune-Mediated Adverse Reactions [see Warnings and Precautions (5.1)]
- Infusion-Related Reactions [see Warnings and Precautions (5.2)]
- Complications of Allogeneic HSCT [see Warnings and Precautions (5.3)]

6.1 Clinical Trials Experience

Because clinical trials are conducted under widely varying conditions, adverse reaction rates observed in the clinical trials of a drug cannot be directly compared to rates in the clinical trials of another drug and may not reflect the rates observed in practice.

The data in WARNINGS AND PRECAUTIONS reflect exposure to OPDIVO as a single agent in 1994 patients enrolled in CHECKMATE-037, CHECKMATE-017, CHECKMATE-057, CHECKMATE-066, CHECKMATE-025, CHECKMATE-067, CHECKMATE-205, CHECKMATE-039 or a single-arm trial in NSCLC (n=117); OPDIVO 1 mg/kg with ipilimumab 3 mg/kg in patients enrolled in CHECKMATE-067 (n=313), CHECKMATE-040 (n=49), or another randomized trial (n=94); OPDIVO 3 mg/kg administered with ipilimumab 1 mg/kg (n=666) in patients enrolled in CHECKMATE-214 or CHECKMATE-142; OPDIVO 3 mg/kg every 2 weeks with ipilimumab 1 mg/kg every 6 weeks in patients enrolled in CHECKMATE-227 (n=576) or CHECKMATE-743 (n=300); OPDIVO 360 mg with ipilimumab 1 mg/kg and 2 cycles of platinum-doublet chemotherapy in CHECKMATE-9LA (n=361); and OPDIVO 240 mg with cabozantinib 40 mg in patients enrolled in CHECKMATE-9ER (n=320).

Unresectable or Metastatic Melanoma

Previously Treated Metastatic Melanoma

The safety of OPDIVO was evaluated in CHECKMATE-037, a randomized, open-label trial in 370 patients with unresectable or metastatic melanoma [see Clinical Studies (14.1)]. Patients had documented disease progression following treatment with ipilimumab and, if BRAF V600 mutation positive, a BRAF inhibitor. The trial excluded patients with autoimmune disease, prior ipilimumab-related Grade 4 adverse reactions (except for endocrinopathies) or Grade 3 ipilimumab-related adverse reactions that had not resolved or were inadequately controlled within 12 weeks of the initiating event, patients with a condition requiring chronic systemic treatment with corticosteroids (>10 mg daily prednisone equivalent) or other immunosuppressive medications, a positive test for hepatitis B or C, and a history of HIV. Patients received OPDIVO 3 mg/kg by intravenous infusion over 60 minutes every 2 weeks (n=268) or investigator’s choice of chemotherapy (n=102): dacarbazine 1000 mg/m^2 intravenously every 3 weeks or carboplatin AUC 6 mg/mL/min and paclitaxel 175 mg/m^2 intravenously every 3 weeks. The median duration of exposure was 5.3 months (range: 1 day to 13.8+ months) in OPDIVO-treated patients and was 2 months (range: 1 day to 9.6+ months) in chemotherapy-treated patients. In this ongoing trial, 24% of patients received OPDIVO for >6 months and 3% of patients received OPDIVO for >1 year.

The population characteristics in the OPDIVO group and the chemotherapy group were similar: 66% male, median age 59.5 years, 98% White, baseline Eastern Cooperative Oncology Group (ECOG) performance status 0 (59%) or 1 (41%), 74% with M1c stage disease, 73% with cutaneous melanoma, 11% with mucosal melanoma, 73% received two or more prior therapies for advanced or metastatic disease, and 18% had brain metastasis. There were more patients in the OPDIVO group with elevated lactate dehydrogenase (LDH) at baseline (51% vs. 38%).

Serious adverse reactions occurred in 41% of patients receiving OPDIVO. OPDIVO was discontinued for adverse reactions in 9% of patients. Twenty-six percent of patients receiving OPDIVO had a dose interruption for an adverse reaction. Grade 3 and 4 adverse reactions occurred in 42% of patients receiving OPDIVO. The most frequent Grade 3 and 4 adverse reactions reported in 2% to <5% of patients receiving OPDIVO were abdominal pain, hyponatremia, increased aspartate aminotransferase, and increased lipase. The most common adverse reaction (reported in ≥20% of patients) was rash.

Tables 5 and 6 summarize the adverse reactions and laboratory abnormalities, respectively, in CHECKMATE-037.

Table 5: Adverse Reactions Occurring in ≥10% of OPDIVO-Treated Patients and at a Higher Incidence than in the Chemotherapy Arm (Between Arm Difference of ≥5% All Grades or ≥2% Grades 3-4) - CHECKMATE-037
Adverse Reaction | OPDIVO (n=268) |  | Chemotherapy (n=102)
Adverse Reaction | All Grades (%) | Grades 3-4 (%) | All Grades (%) | Grades 3-4 (%)
Skin and Subcutaneous Tissue
Rasha | 21 | 0.4 | 7 | 0
Pruritus | 19 | 0 | 3.9 | 0
Respiratory, Thoracic and Mediastinal
Cough | 17 | 0 | 6 | 0
Infections
Upper respiratory tract infectionb | 11 | 0 | 2 | 0
General
Peripheral edema | 10 | 0 | 5 | 0
Toxicity was graded per NCI CTCAE v4.
a Includes maculopapular rash, erythematous rash, pruritic rash, follicular rash, macular rash, papular rash, pustular rash, vesicular rash, and acneiform dermatitis.
b Includes rhinitis, pharyngitis, and nasopharyngitis.

Clinically important adverse reactions in <10% of patients who received OPDIVO were:

Cardiac Disorders: ventricular arrhythmia

Eye Disorders: iridocyclitis

General Disorders and Administration Site Conditions: infusion-related reactions

Investigations: increased amylase, increased lipase

Nervous System Disorders: dizziness, peripheral and sensory neuropathy

Skin and Subcutaneous Tissue Disorders: exfoliative dermatitis, erythema multiforme, vitiligo, psoriasis

Table 6: Laboratory Abnormalities Worsening from Baselinea Occurring in ≥10% of OPDIVO-Treated Patients and at a Higher Incidence than in the Chemotherapy Arm (Between Arm Difference of ≥5% All Grades or ≥2% Grades 3-4) - CHECKMATE-037
Laboratory Abnormality | OPDIVO |  | Chemotherapy
Laboratory Abnormality | All Grades (%) | Grades 3-4 (%) | All Grades (%) | Grades 3-4 (%)
Increased AST | 28 | 2.4 | 12 | 1
Hyponatremia | 25 | 5 | 18 | 1.1
Increased alkaline phosphatase | 22 | 2.4 | 13 | 1.1
Increased ALT | 16 | 1.6 | 5 | 0
Hyperkalemia | 15 | 2 | 6 | 0
a Each test incidence is based on the number of patients who had both baseline and at least one on-study laboratory measurement available: OPDIVO group (range: 252 to 256 patients) and chemotherapy group (range: 94 to 96 patients).

Previously Untreated Metastatic Melanoma

CHECKMATE-066

The safety of OPDIVO was also evaluated in CHECKMATE-066, a randomized, double-blind, active-controlled trial in 411 previously untreated patients with BRAF V600 wild-type unresectable or metastatic melanoma [see Clinical Studies (14.1)]. The trial excluded patients with autoimmune disease and patients requiring chronic systemic treatment with corticosteroids (>10 mg daily prednisone equivalent) or other immunosuppressive medications. Patients received OPDIVO 3 mg/kg by intravenous infusion over 60 minutes every 2 weeks (n=206) or dacarbazine 1000 mg/m^2 intravenously every 3 weeks (n=205). The median duration of exposure was 6.5 months (range: 1 day to 16.6 months) in OPDIVO-treated patients. In this trial, 47% of patients received OPDIVO for >6 months and 12% of patients received OPDIVO for >1 year.

The trial population characteristics in the OPDIVO group and dacarbazine group: 59% male, median age 65 years, 99.5% White, 61% with M1c stage disease, 74% with cutaneous melanoma, 11% with mucosal melanoma, 4% with brain metastasis, and 37% with elevated LDH at baseline. There were more patients in the OPDIVO group with ECOG performance status 0 (71% vs. 59%).

Serious adverse reactions occurred in 36% of patients receiving OPDIVO. Adverse reactions led to permanent discontinuation of OPDIVO in 7% of patients and dose interruption in 26% of patients; no single type of adverse reaction accounted for the majority of OPDIVO discontinuations. Grade 3 and 4 adverse reactions occurred in 41% of patients receiving OPDIVO.

The most frequent Grade 3 and 4 adverse reactions reported in ≥2% of patients receiving OPDIVO were increased gamma-glutamyl transferase (3.9%) and diarrhea (3.4%). The most common adverse reactions (reported in ≥20% of patients and at a higher incidence than in the dacarbazine arm) were fatigue, musculoskeletal pain, rash, and pruritus.

Tables 7 and 8 summarize selected adverse reactions and laboratory abnormalities, respectively, in CHECKMATE-066.

Table 7: Adverse Reactions Occurring in ≥10% of OPDIVO-Treated Patients and at a Higher Incidence than in the Dacarbazine Arm (Between Arm Difference of ≥5% All Grades or ≥2% Grades 3-4) - CHECKMATE-066
Adverse Reaction | OPDIVO (n=206) |  | Dacarbazine (n=205)
Adverse Reaction | All Grades (%) | Grades 3-4 (%) | All Grades (%) | Grades 3-4 (%)
General
Fatigue | 49 | 1.9 | 39 | 3.4
Edemaa | 12 | 1.5 | 4.9 | 0
Musculoskeletal and Connective Tissue
Musculoskeletal painb | 32 | 2.9 | 25 | 2.4
Skin and Subcutaneous Tissue
Rashc | 28 | 1.5 | 12 | 0
Pruritus | 23 | 0.5 | 12 | 0
Vitiligo | 11 | 0 | 0.5 | 0
Erythema | 10 | 0 | 2.9 | 0
Infections
Upper respiratory tract infectiond | 17 | 0 | 6 | 0
Toxicity was graded per NCI CTCAE v4.
a Includes periorbital edema, face edema, generalized edema, gravitational edema, localized edema, peripheral edema, pulmonary edema, and lymphedema.
b Includes back pain, bone pain, musculoskeletal chest pain, musculoskeletal discomfort, myalgia, neck pain, pain in extremity, pain in jaw, and spinal pain.
c Includes maculopapular rash, erythematous rash, pruritic rash, follicular rash, macular rash, papular rash, pustular rash, vesicular rash, dermatitis, allergic dermatitis, exfoliative dermatitis, acneiform dermatitis, drug eruption, and skin reaction.
d Includes rhinitis, viral rhinitis, pharyngitis, and nasopharyngitis.

Clinically important adverse reactions in <10% of patients who received OPDIVO were:

Nervous System Disorders: peripheral neuropathy

Table 8: Laboratory Abnormalities Worsening from Baselinea Occurring in ≥10% of OPDIVO-Treated Patients and at a Higher Incidence than in the Dacarbazine Arm (Between Arm Difference of ≥5% All Grades or ≥2% Grades 3-4) - CHECKMATE-066
Laboratory Abnormality | OPDIVO |  | Dacarbazine
Laboratory Abnormality | All Grades (%) | Grades 3-4 (%) | All Grades (%) | Grades 3-4 (%)
Increased ALT | 25 | 3 | 19 | 0.5
Increased AST | 24 | 3.6 | 19 | 0.5
Increased alkaline phosphatase | 21 | 2.6 | 14 | 1.6
Increased bilirubin | 13 | 3.1 | 6 | 0
a Each test incidence is based on the number of patients who had both baseline and at least one on-study laboratory measurement available: OPDIVO group (range: 194 to 197 patients) and dacarbazine group (range: 186 to 193 patients).

CHECKMATE-067

The safety of OPDIVO, administered with ipilimumab or as a single agent, was evaluated in CHECKMATE-067, a randomized (1:1:1), double-blind trial in 937 patients with previously untreated, unresectable or metastatic melanoma [see Clinical Studies (14.1)]. The trial excluded patients with autoimmune disease, a medical condition requiring systemic treatment with corticosteroids (more than 10 mg daily prednisone equivalent) or other immunosuppressive medication within 14 days of the start of study therapy, a positive test result for hepatitis B or C, or a history of HIV.

Patients were randomized to receive:

- OPDIVO 1 mg/kg over 60 minutes with ipilimumab 3 mg/kg by intravenous infusion every 3 weeks for 4 doses followed by OPDIVO as a single agent at a dose of 3 mg/kg by intravenous infusion over 60 minutes every 2 weeks (OPDIVO and ipilimumab arm; n=313), or
- OPDIVO 3 mg/kg by intravenous infusion over 60 minutes every 2 weeks (OPDIVO arm; n=313), or
- Ipilimumab 3 mg/kg by intravenous infusion every 3 weeks for up to 4 doses (ipilimumab arm; n=311).

The median duration of exposure to OPDIVO was 2.8 months (range: 1 day to 36.4 months) for the OPDIVO and ipilimumab arm and 6.6 months (range: 1 day to 36.0 months) for the OPDIVO arm. In the OPDIVO and ipilimumab arm, 39% were exposed to OPDIVO for ≥6 months and 30% exposed for >1 year. In the OPDIVO arm, 53% were exposed for ≥6 months and 40% for >1 year.

The population characteristics were: 65% male, median age 61 years, 97% White, baseline ECOG performance status 0 (73%) or 1 (27%), 93% with American Joint Committee on Cancer (AJCC) Stage IV disease, 58% with M1c stage disease; 36% with elevated LDH at baseline, 4% with a history of brain metastasis, and 22% had received adjuvant therapy.

Serious adverse reactions (74% and 44%), adverse reactions leading to permanent discontinuation (47% and 18%) or to dosing delays (58% and 36%), and Grade 3 or 4 adverse reactions (72% and 51%) all occurred more frequently in the OPDIVO and ipilimumab arm relative to the OPDIVO arm.

The most frequent (≥10%) serious adverse reactions in the OPDIVO and ipilimumab arm and the OPDIVO arm, respectively, were diarrhea (13% and 2.2%), colitis (10% and 1.9%), and pyrexia (10% and 1%). The most frequent adverse reactions leading to discontinuation of both drugs in the OPDIVO and ipilimumab arm and of OPDIVO in the OPDIVO arm, respectively, were colitis (10% and 0.6%), diarrhea (8% and 2.2%), increased ALT (4.8% and 1%), increased AST (4.5% and 0.6%), and pneumonitis (1.9% and 0.3%).

The most common (≥20%) adverse reactions in the OPDIVO and ipilimumab arm were fatigue, diarrhea, rash, nausea, pyrexia, pruritus, musculoskeletal pain, vomiting, decreased appetite, cough, headache, dyspnea, upper respiratory tract infection, arthralgia, and increased transaminases. The most common (≥20%) adverse reactions in the OPDIVO arm were fatigue, rash, musculoskeletal pain, diarrhea, nausea, cough, pruritus, upper respiratory tract infection, decreased appetite, headache, constipation, arthralgia, and vomiting.

Tables 9 and 10 summarize the incidence of adverse reactions and laboratory abnormalities, respectively, in CHECKMATE-067.

Table 9: Adverse Reactions Occurring in ≥10% of Patients on the OPDIVO and Ipilimumab Arm or the OPDIVO Arm and at a Higher Incidence than in the Ipilimumab Arm (Between Arm Difference of ≥5% All Grades or ≥2% Grades 3-4) - CHECKMATE-067
Adverse Reaction | OPDIVO and Ipilimumab (n=313) |  | OPDIVO (n=313) |  | Ipilimumab (n=311)
Adverse Reaction | All Grades (%) | Grades 3-4 (%) | All Grades (%) | Grades 3-4 (%) | All Grades (%) | Grades 3-4 (%)
General
Fatiguea | 62 | 7 | 59 | 1.6 | 51 | 4.2
Pyrexia | 40 | 1.6 | 16 | 0 | 18 | 0.6
Gastrointestinal
Diarrhea | 54 | 11 | 36 | 5 | 47 | 7
Nausea | 44 | 3.8 | 30 | 0.6 | 31 | 1.9
Vomiting | 31 | 3.8 | 20 | 1 | 17 | 1.6
Skin and Subcutaneous Tissue
Rashb | 53 | 6 | 40 | 1.9 | 42 | 3.5
Vitiligo | 9 | 0 | 10 | 0.3 | 5 | 0
Musculoskeletal and Connective Tissue
Musculoskeletal painc | 32 | 2.6 | 42 | 3.8 | 36 | 1.9
Arthralgia | 21 | 0.3 | 21 | 1 | 16 | 0.3
Metabolism and Nutrition
Decreased appetite | 29 | 1.9 | 22 | 0 | 24 | 1.3
Respiratory, Thoracic and Mediastinal
Cough/productive cough | 27 | 0.3 | 28 | 0.6 | 22 | 0
Dyspnea/exertional dyspnea | 24 | 2.9 | 18 | 1.3 | 17 | 0.6
Infections
Upper respiratory tract infectiond | 23 | 0 | 22 | 0.3 | 17 | 0
Endocrine
Hypothyroidism | 19 | 0.6 | 11 | 0 | 5 | 0
Hyperthyroidism | 11 | 1.3 | 6 | 0 | 1 | 0
Investigations
Decreased weight | 12 | 0 | 7 | 0 | 7 | 0.3
Vascular
Hypertensione | 7 | 2.2 | 11 | 5 | 9 | 2.3
Toxicity was graded per NCI CTCAE v4.
a Includes asthenia and fatigue.
b Includes pustular rash, dermatitis, acneiform dermatitis, allergic dermatitis, atopic dermatitis, bullous dermatitis, exfoliative dermatitis, psoriasiform dermatitis, drug eruption, exfoliative rash, erythematous rash, generalized rash, macular rash, maculopapular rash, morbilliform rash, papular rash, papulosquamous rash, and pruritic rash.
c Includes back pain, bone pain, musculoskeletal chest pain, musculoskeletal discomfort, myalgia, neck pain, pain in extremity, and spinal pain.
d Includes upper respiratory tract infection, nasopharyngitis, pharyngitis, and rhinitis.
e Includes hypertension and blood pressure increased.

Clinically important adverse reactions in <10% of patients who received OPDIVO with ipilimumab or OPDIVO as a single agent were:

Gastrointestinal Disorders: stomatitis, intestinal perforation

Skin and Subcutaneous Tissue Disorders: vitiligo

Musculoskeletal and Connective Tissue Disorders: myopathy, Sjogren’s syndrome, spondyloarthropathy, myositis (including polymyositis)

Nervous System Disorders: neuritis, peroneal nerve palsy

Table 10: Laboratory Abnormalities Worsening from Baselinea Occurring in ≥20% of Patients Treated with OPDIVO with Ipilimumab or Single-Agent OPDIVO and at a Higher Incidence than in the Ipilimumab Arm (Between Arm Difference of ≥5% All Grades or ≥2% Grades 3-4) - CHECKMATE-067
Laboratory Abnormality | OPDIVO and Ipilimumab |  | OPDIVO |  | Ipilimumab
Laboratory Abnormality | All Grades (%) | Grade 3-4 (%) | All Grades (%) | Grade 3-4 (%) | All Grades (%) | Grade 3-4 (%)
Chemistry
Increased ALT | 55 | 16 | 25 | 3 | 29 | 2.7
Hyperglycemia | 53 | 5.3 | 46 | 7 | 26 | 0
Increased AST | 52 | 13 | 29 | 3.7 | 29 | 1.7
Hyponatremia | 45 | 10 | 22 | 3.3 | 26 | 7
Increased lipase | 43 | 22 | 32 | 12 | 24 | 7
Increased alkaline phosphatase | 41 | 6 | 27 | 2 | 23 | 2
Hypocalcemia | 31 | 1.1 | 15 | 0.7 | 20 | 0.7
Increased amylase | 27 | 10 | 19 | 2.7 | 15 | 1.6
Increased creatinine | 26 | 2.7 | 19 | 0.7 | 17 | 1.3
Hematology
Anemia | 52 | 2.7 | 41 | 2.6 | 41 | 6
Lymphopenia | 39 | 5 | 41 | 4.9 | 29 | 4
a Each test incidence is based on the number of patients who had both baseline and at least one on-study laboratory measurement available: OPDIVO and ipilimumab (range: 75 to 297); OPDIVO (range: 81 to 306); ipilimumab (range: 61 to 301).

Adjuvant Treatment of Melanoma

CHECKMATE-76K

The safety of OPDIVO as a single agent was evaluated in CHECKMATE-76K, a randomized (2:1), double-blind trial in 788 patients with completely resected Stage IIB/C melanoma who received OPDIVO 480 mg by intravenous infusion over 30 minutes every 4 weeks (n=524) or placebo by intravenous infusion over 30 minutes every 4 weeks (n=264) for up to 1 year [see Clinical Studies (14.2)]. The median duration of exposure was 11 months in patients treated with OPDIVO and 11 months in patients treated with placebo.

Serious adverse reactions occurred in 18% of patients treated with OPDIVO. A fatal adverse reaction occurred in 1 (0.2%) patient (heart failure and acute kidney injury). Permanent discontinuation of OPDIVO due to an adverse reaction occurred in 17% of patients. Adverse reactions which resulted in permanent discontinuation of OPDIVO in >1% of patients included diarrhea (1.1%), arthralgia (1.7%), and rash (1.7%).

Dosage interruptions of OPDIVO due to an adverse reaction occurred in 25% of patients. Adverse reactions which required dosage interruption in >1% of patients included COVID-19 infection, infusion related reaction, diarrhea, arthralgia, and increased ALT.

The most common adverse reactions (reported in ≥20% of patients) were fatigue, musculoskeletal pain, rash, diarrhea, and pruritus.

Tables 11 and 12 summarize the adverse reactions and laboratory abnormalities, respectively, in CHECKMATE-76K.

Table 11: Adverse Reactions Occurring in ≥10% of Patients Treated with OPDIVO - CHECKMATE-76K
Adverse Reaction | OPDIVO (n=524) |  | Placebo (n=264)
Adverse Reaction | All Grades (%) | Grades 3-4 (%) | All Grades (%) | Grades 3-4 (%)
General
Fatiguea | 36 | 0.4 | 34 | 0.4
Musculoskeletal and connective tissue
Musculoskeletal painb | 30 | 0.4 | 26 | 0.4
Skin and Subcutaneous Tissue
Rashc | 28 | 1.1 | 15 | 0.4
Pruritus | 20 | 0.2 | 11 | 0
Gastrointestinal
Diarrhead | 23 | 1.3 | 16 | 0
Nausea | 14 | 0 | 11 | 0
Endocrine
Hypothyroidisme | 14 | 0 | 2.3 | 0
Nervous system
Headachef | 12 | 0.2 | 14 | 0.8
Toxicity was graded per NCI CTCAE v5.
a Includes asthenia.
b Includes arthralgia, arthritis, back pain, bone pain, musculoskeletal chest pain, musculoskeletal discomfort, musculoskeletal stiffness, myalgia, neck pain, non-cardiac chest pain, spinal pain, pain in extremity.
c Includes dermatitis, dermatitis acneiform, dyshidrotic eczema, eczema, eczema asteatotic, eyelid rash, genital rash, pemphigoid, penile rash, rash erythematous, rash follicular, rash macular, rash maculo-papular, rash papular, rash pruritic, rash pustular, rash vesicular, skin exfoliation, toxic skin eruption.
d Includes autoimmune colitis, colitis, diarrhea, enteritis, enterocolitis.
e Includes autoimmune hypothyroidism, blood thyroid stimulating hormone increased.
f Includes cluster headache, migraine.

Table 12: Laboratory Abnormalities Worsening from Baselinea Occurring in ≥10% of OPDIVO-Treated Patients - CHECKMATE-76K
Laboratory Abnormality | OPDIVO (n=524) |  | Placebo (n=264)
Laboratory Abnormality | All Grades (%) | Grades 3-4 (%) | All Grades (%) | Grades 3-4 (%)
Hematology
Anemia | 19 | 0 | 14 | 0
Lymphopenia | 17 | 1.1 | 17 | 1.7
Neutropenia | 10 | 0 | 10 | 0.4
Chemistry
AST increased | 25 | 2.2 | 16 | 0.4
Lipase increased | 22 | 2.9 | 21 | 2.3
ALT increased | 20 | 2.1 | 15 | 0.4
Amylase increased | 17 | 0.4 | 9 | 0
Creatinine increased | 15 | 0.4 | 13 | 0
Sodium decreased | 13 | 0.6 | 11 | 0.4
Potassium increased | 13 | 1 | 15 | 1.1
a Each test incidence is based on the number of patients who had both baseline and at least one on-study laboratory measurement available: OPDIVO group (range: 262 to 513 patients) and placebo group (range: 138 to 261 patients).

CHECKMATE-238

The safety of OPDIVO as a single agent was evaluated in CHECKMATE-238, a randomized (1:1), double-blind trial in 905 patients with completely resected Stage IIIB/C or Stage IV melanoma received OPDIVO 3 mg/kg by intravenous infusion over 60 minutes every 2 weeks (n=452) or ipilimumab 10 mg/kg by intravenous infusion every 3 weeks for 4 doses then every 12 weeks beginning at Week 24 for up to 1 year (n=453) [see Clinical Studies (14.2)]. The median duration of exposure was 11.5 months in OPDIVO-treated patients and was 2.7 months in ipilimumab-treated patients. In this ongoing trial, 74% of patients received OPDIVO for >6 months.

Serious adverse reactions occurred in 18% of OPDIVO-treated patients. Study therapy was discontinued for adverse reactions in 9% of OPDIVO-treated patients and 42% of ipilimumab-treated patients. Twenty-eight percent of OPDIVO-treated patients had at least one omitted dose for an adverse reaction. Grade 3 or 4 adverse reactions occurred in 25% of OPDIVO-treated patients.

The most frequent Grade 3 and 4 adverse reactions reported in ≥2% of OPDIVO-treated patients were diarrhea and increased lipase and amylase. The most common adverse reactions (at least 20%) were fatigue, diarrhea, rash, musculoskeletal pain, pruritus, headache, nausea, upper respiratory infection, and abdominal pain. The most common immune-mediated adverse reactions were rash (16%), diarrhea/colitis (6%), and hepatitis (3%).

Tables 13 and 14 summarize the adverse reactions and laboratory abnormalities, respectively, in CHECKMATE-238.

Table 13: Adverse Reactions Occurring in ≥10% of OPDIVO-Treated Patients - CHECKMATE-238
Adverse Reaction | OPDIVO (n=452) |  | Ipilimumab 10 mg/kg (n=453)
Adverse Reaction | All Grades (%) | Grades 3-4 (%) | All Grades (%) | Grades 3-4 (%)
General
Fatiguea | 57 | 0.9 | 55 | 2.4
Gastrointestinal
Diarrhea | 37 | 2.4 | 55 | 11
Nausea | 23 | 0.2 | 28 | 0
Abdominal painb | 21 | 0.2 | 23 | 0.9
Constipation | 10 | 0 | 9 | 0
Skin and Subcutaneous Tissue
Rashc | 35 | 1.1 | 47 | 5.3
Pruritus | 28 | 0 | 37 | 1.1
Musculoskeletal and Connective Tissue
Musculoskeletal paind | 32 | 0.4 | 27 | 0.4
Arthralgia | 19 | 0.4 | 13 | 0.4
Nervous System
Headache | 23 | 0.4 | 31 | 2.0
Dizzinesse | 11 | 0 | 8 | 0
Infections
Upper respiratory tract infectionf | 22 | 0 | 15 | 0.2
Respiratory, Thoracic and Mediastinal
Cough/productive cough | 19 | 0 | 19 | 0
Dyspnea/exertional dyspnea | 10 | 0.4 | 10 | 0.2
Endocrine
Hypothyroidismg | 12 | 0.2 | 7.5 | 0.4
Toxicity was graded per NCI CTCAE v4.
a Includes asthenia.
b Includes abdominal discomfort, lower abdominal pain, upper abdominal pain, and abdominal tenderness.
c Includes dermatitis described as acneiform, allergic, bullous, or exfoliative and rash described as generalized, erythematous, macular, papular, maculopapular, pruritic, pustular, vesicular, or butterfly, and drug eruption.
d Includes back pain, bone pain, musculoskeletal chest pain, musculoskeletal discomfort, myalgia, neck pain, spinal pain, and pain in extremity.
e Includes postural dizziness and vertigo.
f Includes upper respiratory tract infection including viral respiratory tract infection, lower respiratory tract infection, rhinitis, pharyngitis, and nasopharyngitis.
g Includes secondary hypothyroidism and autoimmune hypothyroidism.

Table 14: Laboratory Abnormalities Worsening from Baselinea Occurring in ≥10% of OPDIVO-Treated Patients - CHECKMATE-238
Laboratory Abnormality | OPDIVO |  | Ipilimumab 10 mg/kg
Laboratory Abnormality | All Grades (%) | Grades 3-4 (%) | All Grades (%) | Grades 3-4 (%)
Hematology
Lymphopenia | 27 | 0.4 | 12 | 0.9
Anemia | 26 | 0 | 34 | 0.5
Leukopenia | 14 | 0 | 2.7 | 0.2
Neutropenia | 13 | 0 | 6 | 0.5
Chemistry
Increased Lipase | 25 | 7 | 23 | 9
Increased ALT | 25 | 1.8 | 40 | 12
Increased AST | 24 | 1.3 | 33 | 9
Increased Amylase | 17 | 3.3 | 13 | 3.1
Hyponatremia | 16 | 1.1 | 22 | 3.2
Hyperkalemia | 12 | 0.2 | 9 | 0.5
Increased Creatinine | 12 | 0 | 13 | 0
Hypocalcemia | 10 | 0.7 | 16 | 0.5
a Each test incidence is based on the number of patients who had both baseline and at least one on-study laboratory measurement available: OPDIVO group (range: 400 to 447 patients) and ipilimumab 10 mg/kg group (range: 392 to 443 patients).

Neoadjuvant Treatment of Resectable (Tumors ≥4 cm or Node Positive) Non-Small Cell Lung Cancer

The safety of OPDIVO in combination with platinum-doublet chemotherapy was evaluated in CHECKMATE-816, a randomized, open-label, multicenter trial in patients with resectable NSCLC [see Clinical Studies (14.3)]. Patients received either OPDIVO 360 mg administered in combination with platinum-doublet chemotherapy administered every 3 weeks for 3 cycles; or platinum-doublet chemotherapy administered every 3 weeks for 3 cycles.

The median age of patients who received OPDIVO in combination with platinum-doublet chemotherapy or platinum-doublet chemotherapy was 65 years (range: 34 – 84); 72% male; 47% White, 50% Asian, and 2% Black/African American.

Serious adverse reactions occurred in 30% of patients who were treated with OPDIVO in combination with platinum-doublet chemotherapy. Serious adverse reactions in >2% included pneumonia and vomiting. No fatal adverse reactions occurred in patients who received OPDIVO in combination with platinum-doublet chemotherapy.

Study therapy with OPDIVO in combination with platinum-doublet chemotherapy was permanently discontinued for adverse reactions in 10% of patients and 30% had at least one treatment withheld for an adverse reaction. The most common adverse reactions (≥1%) resulting in permanent discontinuation of OPDIVO in combination with platinum-doublet chemotherapy were anaphylactic reaction (1.7%), acute kidney injury (1.1%), rash (1.1%), and fatigue (1.1%).

The most common (>20%) adverse reactions were nausea, constipation, fatigue, decreased appetite, and rash. The most common Grade 3 or 4 laboratory abnormalities (≥2%) were neutropenia, hyperglycemia, leukopenia, lymphopenia, increased amylase, anemia, thrombocytopenia, and hyponatremia.

Tables 15 and 16 summarize selected adverse reactions and laboratory abnormalities, respectively, in CHECKMATE-816.

Table 15: Adverse Reactions in >10% of Patients with Early-Stage NSCLC Receiving Neoadjuvant OPDIVO and Platinum-Doublet Chemotherapy in CHECKMATE-816
Adverse Reaction | OPDIVO and Platinum-Doublet Chemotherapy (n=176) |  | Platinum-Doublet Chemotherapy (n=176)
Adverse Reaction | All Grades; (%) | Grades 3 or 4 (%) | All Grades; (%) | Grades 3 or 4 (%)
Gastrointestinal
Nausea | 38 | 0.6 | 45 | 1.1
Constipation | 34 | 0 | 32 | 1.1
Vomiting | 11 | 1.1 | 13 | 0.6
General
Fatiguea | 26 | 2.3 | 23 | 1.1
Malaise | 15 | 0.6 | 14 | 0.6
Metabolism and Nutrition
Decreased appetite | 20 | 1.1 | 23 | 2.3
Skin and Subcutaneous Tissue
Rashb | 20 | 2.3 | 7 | 0
Alopecia | 11 | 0 | 15 | 0
Nervous System
Peripheral neuropathyc | 13 | 0 | 6 | 0
Toxicity was graded per NCI CTCAE v4.
a Includes fatigue and asthenia.
b Includes rash, dermatitis, acneiform dermatitis, atopic dermatitis, bullous dermatitis, drug eruption, maculopapular rash, and pruritic rash.
c Includes peripheral neuropathy, dysesthesia, hypoesthesia, peripheral motor neuropathy, peripheral sensory neuropathy.

Table 16: Select Laboratory Values Worsening from Baselinea Occurring in >20% of Patients with Early-Stage NSCLC Receiving Neoadjuvant OPDIVO and Platinum-Doublet Chemotherapy in CHECKMATE-816
Laboratory Abnormality | OPDIVO and Platinum-Doublet Chemotherapya |  | Platinum-Doublet Chemotherapya
Laboratory Abnormality | All Grades; (%) | Grades 3 or 4 (%) | All Grades; (%) | Grades 3 or 4 (%)
Hematology
Anemia | 63 | 3.5 | 70 | 6
Neutropenia | 58 | 22 | 58 | 27
Leukopenia | 53 | 5 | 51 | 11
Lymphopenia | 38 | 4.7 | 31 | 1.8
Thrombocytopenia | 24 | 2.9 | 22 | 3
Chemistry
Hyperglycemia | 37 | 6 | 35 | 2.9
Hypomagnesemia | 25 | 1.2 | 29 | 1.2
Hyponatremia | 25 | 2.4 | 28 | 1.8
Increased amylase | 23 | 3.6 | 13 | 1.8
Increased ALT | 23 | 0 | 20 | 1.2
a Each test incidence is based on the number of patients who had both baseline and at least one on-study laboratory measurement available: OPDIVO and platinum-doublet chemotherapy group (range: 73 to 171 patients) and platinum-doublet chemotherapy group (range: 68 to 171 patients).

Neoadjuvant and Adjuvant Treatment of Resectable Non-Small Cell Lung Cancer

The safety of OPDIVO in combination with neoadjuvant platinum-doublet chemotherapy followed by surgery and continued adjuvant treatment with OPDIVO as a single agent after surgery was evaluated in CHECKMATE-77T, a randomized, double-blind, multicenter trial in patients with previously untreated resectable Stage IIA (> 4 cm) to IIIB (T3N2 or T4N2) NSCLC (per the AJCC Cancer Staging Manual 8th Edition) [see Clinical Studies (14.4)]. Patients with active autoimmune disease or a medical condition that required immunosuppression were ineligible. The median duration of exposure to OPDIVO was 10.3 months (range: 1 day to 22.3 months).

The study population characteristics were: median age 66 years (range: 35 - 86); 71% male; 72% White, 25% Asian, 1.7% Black/African American, and 1.5% other race; and 6% Hispanic or Latino.

Adverse reactions occurring in patients with resectable NSCLC receiving OPDIVO in combination with platinum-doublet chemotherapy, given as neoadjuvant treatment and followed as a single agent adjuvant treatment after surgery, were generally similar to those occurring in patients in other clinical trials across tumor types receiving OPDIVO in combination with chemotherapy.

Neoadjuvant Phase of CHECKMATE-77T

A total of 228 patients received at least 1 dose of OPDIVO in combination with platinum-doublet chemotherapy as neoadjuvant treatment and 230 patients received at least 1 dose of placebo in combination with platinum-doublet chemotherapy as neoadjuvant treatment.

Serious adverse reactions occurred in 21% of patients who received OPDIVO in combination with platinum-doublet chemotherapy as neoadjuvant treatment; the most frequent (≥2%) serious adverse reactions was pneumonia. Fatal adverse reactions occurred in 2.2% of patients, due to cerebrovascular accident, COVID-19 infection, hemoptysis, pneumonia, and pneumonitis (0.4% each).

Permanent discontinuation of any study drug due to an adverse reaction occurred in 13% of patients who received OPDIVO in combination with platinum-doublet chemotherapy as neoadjuvant treatment; the most frequent (≥1%) adverse reaction that led to permanent discontinuation of any study drug was peripheral sensory neuropathy (2.2%).

Of the 228 OPDIVO-treated patients and 230 placebo-treated patients who received neoadjuvant treatment, 5.3% (n=12) and 3.5% (n=8), respectively, did not receive surgery due to adverse reactions. The adverse reactions that led to cancellation of surgery in OPDIVO-treated patients were cerebrovascular accident, pneumonia, and colitis/diarrhea (2 patients each) and acute coronary syndrome, myocarditis, hemoptysis, pneumonitis, COVID-19, and myositis (1 patient each).

Of the 178 OPDIVO-treated patients who received surgery, 4.5% (n=8) experienced delay of surgery (surgery more than 6 weeks from last neoadjuvant treatment) due to adverse reactions. Of the 178 placebo-treated patients who received surgery, 3.9% (n=7) experienced delay of surgery due to adverse reactions.

Of the 178 OPDIVO-treated patients who received surgery, 7% (n=13) did not receive adjuvant treatment due to adverse reactions. Of the 178 placebo-treated patients who received surgery, 2.8% (n=5) did not receive adjuvant treatment due to adverse reactions.

Adjuvant Phase of CHECKMATE-77T

A total of 142 patients in the OPDIVO arm and 152 patients in the placebo arm received at least 1 dose of adjuvant treatment.

Of the patients who received single agent OPDIVO as adjuvant treatment, 22% experienced serious adverse reactions; the most frequent serious adverse reaction was pneumonitis/ILD (2.8%). One fatal adverse reaction due to COVID-19 occurred. Permanent discontinuation of adjuvant OPDIVO due to an adverse reaction occurred in 14% of patients; the most frequent (≥1%) adverse reactions that led to permanent discontinuation of adjuvant OPDIVO were pneumonitis (4.2%) and diarrhea (1.4%).

Metastatic Non-Small Cell Lung Cancer

First-line Treatment of Metastatic NSCLC: In Combination with Ipilimumab

The safety of OPDIVO in combination with ipilimumab was evaluated in CHECKMATE-227, a randomized, multicenter, multi-cohort, open-label trial in patients with previously untreated metastatic or recurrent NSCLC with no EGFR or ALK genomic tumor aberrations [see Clinical Studies (14.5)]. The trial excluded patients with untreated brain metastases, carcinomatous meningitis, active autoimmune disease, or medical conditions requiring systemic immunosuppression. Patients received OPDIVO 3 mg/kg by intravenous infusion over 30 minutes every 2 weeks and ipilimumab 1 mg/kg by intravenous infusion over 30 minutes every 6 weeks or platinum-doublet chemotherapy every 3 weeks for 4 cycles. The median duration of therapy in OPDIVO and ipilimumab-treated patients was 4.2 months (range: 1 day to 25.5 months): 39% of patients received OPDIVO and ipilimumab for >6 months and 23% of patients received OPDIVO and ipilimumab for >1 year. The population characteristics were: median age 64 years (range: 26 to 87); 48% were ≥65 years of age, 76% White, and 67% male. Baseline ECOG performance status was 0 (35%) or 1 (65%), 85% were former/current smokers, 11% had brain metastases, 28% had squamous histology and 72% had non-squamous histology.

Serious adverse reactions occurred in 58% of patients. OPDIVO and ipilimumab were discontinued for adverse reactions in 24% of patients and 53% had at least one dose withheld for an adverse reaction.

The most frequent (≥2%) serious adverse reactions were pneumonia, diarrhea/colitis, pneumonitis, hepatitis, pulmonary embolism, adrenal insufficiency, and hypophysitis. Fatal adverse reactions occurred in 1.7% of patients; these included events of pneumonitis (4 patients), myocarditis, acute kidney injury, shock, hyperglycemia, multi-system organ failure, and renal failure. The most common (≥20%) adverse reactions were fatigue, rash, decreased appetite, musculoskeletal pain, diarrhea/colitis, dyspnea, cough, hepatitis, nausea, and pruritus.

Tables 17 and 18 summarize selected adverse reactions and laboratory abnormalities, respectively, in CHECKMATE-227.

Table 17: Adverse Reactions in ≥10% of Patients Receiving OPDIVO and Ipilimumab - CHECKMATE-227
Adverse Reaction | OPDIVO and Ipilimumab (n=576) |  | Platinum-Doublet Chemotherapy (n=570)
Adverse Reaction | All Grades (%) | Grades 3-4 (%) | All Grades (%) | Grades 3-4 (%)
General
Fatiguea | 44 | 6 | 42 | 4.4
Pyrexia | 18 | 0.5 | 11 | 0.4
Edemab | 14 | 0.2 | 12 | 0.5
Skin and Subcutaneous Tissue
Rashc | 34 | 4.7 | 10 | 0.4
Pruritusd | 21 | 0.5 | 3.3 | 0
Metabolism and Nutrition
Decreased appetite | 31 | 2.3 | 26 | 1.4
Musculoskeletal and Connective Tissue
Musculoskeletal paine | 27 | 1.9 | 16 | 0.7
Arthralgia | 13 | 0.9 | 2.5 | 0.2
Gastrointestinal
Diarrhea/colitisf | 26 | 3.6 | 16 | 0.9
Nausea | 21 | 1 | 42 | 2.5
Constipation | 18 | 0.3 | 27 | 0.5
Vomiting | 13 | 1 | 18 | 2.3
Abdominal paing | 10 | 0.2 | 9 | 0.7
Respiratory, Thoracic, and Mediastinal
Dyspneah | 26 | 4.3 | 16 | 2.1
Coughi | 23 | 0.2 | 13 | 0
Hepatobiliary
Hepatitisj | 21 | 9 | 10 | 1.2
Endocrine
Hypothyroidismk | 16 | 0.5 | 1.2 | 0
Hyperthyroidisml | 10 | 0 | 0.5 | 0
Infections and Infestations
Pneumoniam | 13 | 7 | 8 | 4
Nervous System
Headache | 11 | 0.5 | 6 | 0
a Includes fatigue and asthenia.
b Includes eyelid edema, face edema, generalized edema, localized edema, edema, edema peripheral, and periorbital edema.
c Includes autoimmune dermatitis, dermatitis, dermatitis acneiform, dermatitis allergic, dermatitis atopic, dermatitis bullous, dermatitis contact, dermatitis exfoliative, dermatitis psoriasiform, granulomatous dermatitis, rash generalized, drug eruption, dyshidrotic eczema, eczema, exfoliative rash, nodular rash, rash, rash erythematous, rash macular, rash maculo-papular, rash papular, rash pruritic, rash pustular, toxic skin eruption.
d Includes pruritus and pruritus generalized.
e Includes back pain, bone pain, musculoskeletal chest pain, musculoskeletal discomfort, musculoskeletal pain, myalgia, and pain in extremity.
f Includes colitis, colitis microscopic, colitis ulcerative, diarrhea, enteritis infectious, enterocolitis, enterocolitis infectious, and enterocolitis viral.
g Includes abdominal discomfort, abdominal pain, abdominal pain lower, abdominal pain upper, and abdominal tenderness.
h Includes dyspnea and dyspnea exertional.
i Includes cough and productive cough.
j Includes alanine aminotransferase increased, aspartate aminotransferase increased, autoimmune hepatitis, blood bilirubin increased, hepatic enzyme increased, hepatic failure, hepatic function abnormal, hepatitis, hepatitis E, hepatocellular injury, hepatotoxicity, hyperbilirubinemia, immune-mediated hepatitis, liver function test abnormal, liver function test increased, transaminases increased.
k Includes autoimmune thyroiditis, blood thyroid stimulating hormone increased, hypothyroidism, primary hypothyroidism, thyroiditis, and tri-iodothyronine free decreased.
l Contains blood thyroid stimulating hormone decreased, hyperthyroidism, and tri-iodothyronine free increased.
m Includes lower respiratory tract infection, lower respiratory tract infection bacterial, lung infection, pneumonia, pneumonia adenoviral, pneumonia aspiration, pneumonia bacterial, pneumonia klebsiella, pneumonia influenzal, pneumonia viral, atypical pneumonia, organizing pneumonia.

Other clinically important adverse reactions in CHECKMATE-227 were:

Skin and Subcutaneous Tissue: urticaria, alopecia, erythema multiforme, vitiligo

Gastrointestinal: stomatitis, pancreatitis, gastritis

Musculoskeletal and Connective Tissue: arthritis, polymyalgia rheumatica, rhabdomyolysis

Nervous System: peripheral neuropathy, autoimmune encephalitis

Blood and Lymphatic System: eosinophilia

Eye Disorders: blurred vision, uveitis

Cardiac: atrial fibrillation, myocarditis

Table 18: Laboratory Values Worsening from Baselinea Occurring in ≥20% of Patients on OPDIVO and Ipilimumab - CHECKMATE-227
Laboratory Abnormality | OPDIVO and Ipilimumab |  | Platinum-Doublet Chemotherapy
Laboratory Abnormality | Grades 1-4 (%) | Grades 3-4 (%) | Grades 1-4 (%) | Grades 3-4 (%)
Hematology
Anemia | 46 | 3.6 | 78 | 14
Lymphopenia | 46 | 5 | 60 | 15
Chemistry
Hyponatremia | 41 | 12 | 26 | 4.9
Increased AST | 39 | 5 | 26 | 0.4
Increased ALT | 36 | 7 | 27 | 0.7
Increased lipase | 35 | 14 | 14 | 3.4
Increased alkaline phosphatase | 34 | 3.8 | 20 | 0.2
Increased amylase | 28 | 9 | 18 | 1.9
Hypocalcemia | 28 | 1.7 | 17 | 1.3
Hyperkalemia | 27 | 3.4 | 22 | 0.4
Increased creatinine | 22 | 0.9 | 17 | 0.2
a Each test incidence is based on the number of patients who had both baseline and at least one on-study laboratory measurement available: OPDIVO and ipilimumab group (range: 494 to 556 patients) and chemotherapy group (range: 469 to 542 patients).

First-line Treatment of Metastatic or Recurrent NSCLC: In Combination with Ipilimumab and Platinum-Doublet Chemotherapy

The safety of OPDIVO in combination with ipilimumab and platinum-doublet chemotherapy was evaluated in CHECKMATE-9LA [see Clinical Studies (14.5)]. Patients received either OPDIVO 360 mg administered every 3 weeks in combination with ipilimumab 1 mg/kg administered every 6 weeks and platinum-doublet chemotherapy administered every 3 weeks for 2 cycles; or platinum-doublet chemotherapy administered every 3 weeks for 4 cycles. The median duration of therapy in OPDIVO in combination with ipilimumab and platinum-doublet chemotherapy was 6 months (range: 1 day to 19 months): 50% of patients received OPDIVO and ipilimumab for >6 months and 13% of patients received OPDIVO and ipilimumab for >1 year.

Serious adverse reactions occurred in 57% of patients who were treated with OPDIVO in combination with ipilimumab and platinum-doublet chemotherapy. The most frequent (>2%) serious adverse reactions were pneumonia, diarrhea, febrile neutropenia, anemia, acute kidney injury, musculoskeletal pain, dyspnea, pneumonitis, and respiratory failure. Fatal adverse reactions occurred in 7 (2%) patients, and included hepatic toxicity, acute renal failure, sepsis, pneumonitis, diarrhea with hypokalemia, and massive hemoptysis in the setting of thrombocytopenia.

Study therapy with OPDIVO in combination with ipilimumab and platinum-doublet chemotherapy was permanently discontinued for adverse reactions in 24% of patients and 56% had at least one treatment withheld for an adverse reaction. The most common (>20%) adverse reactions were fatigue, musculoskeletal pain, nausea, diarrhea, rash, decreased appetite, constipation, and pruritus.

Tables 19 and 20 summarize selected adverse reactions and laboratory abnormalities, respectively, in CHECKMATE-9LA.

Table 19: Adverse Reactions in >10% of Patients Receiving OPDIVO and Ipilimumab and Platinum-Doublet Chemotherapy - CHECKMATE-9LA
Adverse Reaction | OPDIVO and Ipilimumab and Platinum-Doublet Chemotherapy (n=358) |  | Platinum-Doublet Chemotherapy (n=349)
Adverse Reaction | All Grades (%) | Grades 3-4 (%) | All Grades (%) | Grades 3-4 (%)
General
Fatiguea | 49 | 5 | 40 | 4.9
Pyrexia | 14 | 0.6 | 10 | 0.6
Musculoskeletal and Connective Tissue
Musculoskeletal painb | 39 | 4.5 | 27 | 2
Gastrointestinal
Nausea | 32 | 1.7 | 41 | 0.9
Diarrheac | 31 | 6 | 18 | 1.7
Constipation | 21 | 0.6 | 23 | 0.6
Vomiting | 18 | 2 | 17 | 1.4
Abdominal paind | 12 | 0.6 | 11 | 0.9
Skin and Subcutaneous Tissue
Rashe | 30 | 4.7 | 10 | 0.3
Pruritusf | 21 | 0.8 | 2.9 | 0
Alopecia | 11 | 0.8 | 10 | 0.6
Metabolism and Nutrition
Decreased appetite | 28 | 2 | 22 | 1.7
Respiratory, Thoracic and Mediastinal
Coughg | 19 | 0.6 | 15 | 0.9
Dyspneah | 18 | 4.7 | 14 | 3.2
Endocrine
Hypothyroidismi | 19 | 0.3 | 3.4 | 0
Nervous System
Headache | 11 | 0.6 | 7 | 0
Dizzinessj | 11 | 0.6 | 6 | 0
Toxicity was graded per NCI CTCAE v4.
a Includes fatigue and asthenia.
b Includes myalgia, back pain, pain in extremity, musculoskeletal pain, bone pain, flank pain, muscle spasms, musculoskeletal chest pain, musculoskeletal disorder, osteitis, musculoskeletal stiffness, non-cardiac chest pain, arthralgia, arthritis, arthropathy, joint effusion, psoriatic arthropathy, synovitis.
c Includes colitis, ulcerative colitis, diarrhea, and enterocolitis.
d Includes abdominal discomfort, abdominal pain, lower abdominal pain, upper abdominal pain, and gastrointestinal pain.
e Includes acne, dermatitis, acneiform dermatitis, allergic dermatitis, atopic dermatitis, bullous dermatitis, generalized exfoliative dermatitis, eczema, keratoderma blennorrhagica, palmar-plantar erythrodysesthesia syndrome, rash, erythematous rash, generalized rash, macular rash, maculo-papular rash, morbilliform rash, papular rash, pruritic rash, skin exfoliation, skin reaction, skin toxicity, Stevens-Johnson syndrome, urticaria.
f Includes pruritus and generalized pruritus.
g Includes cough, productive cough, and upper-airway cough syndrome.
h Includes dyspnea, dyspnea at rest, and exertional dyspnea.
i Includes autoimmune thyroiditis, increased blood thyroid stimulating hormone, hypothyroidism, thyroiditis, and decreased free tri-iodothyronine.
j Includes dizziness, vertigo and positional vertigo.

Table 20: Laboratory Values Worsening from Baselinea Occurring in >20% of Patients on OPDIVO and Ipilimumab and Platinum-Doublet Chemotherapy - CHECKMATE-9LA
Laboratory Abnormality | OPDIVO and Ipilimumab and Platinum-Doublet Chemotherapy |  | Platinum-Doublet Chemotherapy
Laboratory Abnormality | Grades 1-4 (%) | Grades 3-4 (%) | Grades 1-4 (%) | Grades 3-4 (%)
Hematology
Anemia | 70 | 9 | 74 | 16
Lymphopenia | 41 | 6 | 40 | 11
Neutropenia | 40 | 15 | 42 | 15
Leukopenia | 36 | 10 | 40 | 9
Thrombocytopenia | 23 | 4.3 | 24 | 5
Chemistry
Hyperglycemia | 45 | 7 | 42 | 2.6
Hyponatremia | 37 | 10 | 27 | 7
Increased ALT | 34 | 4.3 | 24 | 1.2
Increased lipase | 31 | 12 | 10 | 2.2
Increased alkaline phosphatase | 31 | 1.2 | 26 | 0.3
Increased amylase | 30 | 7 | 19 | 1.3
Increased AST | 30 | 3.5 | 22 | 0.3
Hypomagnesemia | 29 | 1.2 | 33 | 0.6
Hypocalcemia | 26 | 1.4 | 22 | 1.8
Increased creatinine | 26 | 1.2 | 23 | 0.6
Hyperkalemia | 22 | 1.7 | 21 | 2.1
a Each test incidence is based on the number of patients who had both baseline and at least one on-study laboratory measurement available: OPDIVO and ipilimumab and platinum-doublet chemotherapy group (range: 197 to 347 patients) and platinum-doublet chemotherapy group (range: 191 to 335 patients).

Second-line Treatment of Metastatic NSCLC

The safety of OPDIVO was evaluated in CHECKMATE-017, a randomized open-label, multicenter trial in patients with metastatic squamous NSCLC and progression on or after one prior platinum doublet-based chemotherapy regimen and in CHECKMATE-057, a randomized, open-label, multicenter trial in patients with metastatic non-squamous NSCLC and progression on or after one prior platinum doublet-based chemotherapy regimen [see Clinical Studies (14.5)]. These trials excluded patients with active autoimmune disease, medical conditions requiring systemic immunosuppression, or with symptomatic interstitial lung disease. Patients received OPDIVO 3 mg/kg over 60 minutes by intravenous infusion every 2 weeks or docetaxel 75 mg/m^2 intravenously every 3 weeks. The median duration of therapy in OPDIVO-treated patients in CHECKMATE-017 was 3.3 months (range: 1 day to 21.7+ months) and in CHECKMATE-057 was 2.6 months (range: 0 to 24.0+ months). In CHECKMATE-017, 36% of patients received OPDIVO for at least 6 months and 18% of patients received OPDIVO for at least 1 year and in CHECKMATE-057, 30% of patients received OPDIVO for >6 months and 20% of patients received OPDIVO for >1 year.

Across both trials, the median age of OPDIVO-treated patients was 61 years (range: 37 to 85); 38% were ≥65 years of age, 61% were male, and 91% were White. Ten percent of patients had brain metastases and ECOG performance status was 0 (26%) or 1 (74%).

In CHECKMATE-057, in the OPDIVO arm, seven deaths were due to infection including one case of Pneumocystis jirovecii pneumonia, four were due to pulmonary embolism, and one death was due to limbic encephalitis. Serious adverse reactions occurred in 46% of patients receiving OPDIVO. OPDIVO was discontinued in 11% of patients and was delayed in 28% of patients for an adverse reaction.

The most frequent serious adverse reactions reported in ≥2% of patients receiving OPDIVO were pneumonia, pulmonary embolism, dyspnea, pyrexia, pleural effusion, pneumonitis, and respiratory failure. Across both trials, the most common adverse reactions (≥20%) were fatigue, musculoskeletal pain, cough, dyspnea, and decreased appetite.

Tables 21 and 22 summarize selected adverse reactions and laboratory abnormalities, respectively, in CHECKMATE-057.

Table 21: Adverse Reactions Occurring in ≥10% of OPDIVO-Treated Patients and at a Higher Incidence than Docetaxel (Between Arm Difference of ≥5% All Grades or ≥2% Grades 3-4) - CHECKMATE-017 and CHECKMATE-057
Adverse Reaction | OPDIVO (n=418) |  | Docetaxel (n=397)
Adverse Reaction | All Grades (%) | Grades 3-4 (%) | All Grades (%) | Grades 3-4 (%)
Respiratory, Thoracic and Mediastinal
Cough | 31 | 0.7 | 24 | 0
Metabolism and Nutrition
Decreased appetite | 28 | 1.4 | 23 | 1.5
Skin and Subcutaneous Tissue
Pruritus | 10 | 0.2 | 2 | 0
Toxicity was graded per NCI CTCAE v4.

Other clinically important adverse reactions observed in OPDIVO-treated patients and which occurred at a similar incidence in docetaxel-treated patients and not listed elsewhere in section 6 include: fatigue/asthenia (48% all Grades, 5% Grade 3-4), musculoskeletal pain (33% all Grades), pleural effusion (4.5% all Grades), pulmonary embolism (3.3% all Grades).

Table 22: Laboratory Abnormalities Worsening from Baselinea Occurring in ≥10% of OPDIVO-Treated Patients for all NCI CTCAE Grades and at a Higher Incidence than Docetaxel (Between Arm Difference of ≥5% All Grades or ≥2% Grades 3-4) - CHECKMATE-017 and CHECKMATE-057
Laboratory Abnormality | OPDIVO |  | Docetaxel
Laboratory Abnormality | All Grades (%) | Grades 3-4 (%) | All Grades (%) | Grades 3-4 (%)
Chemistry
Hyponatremia | 35 | 7 | 34 | 4.9
Increased AST | 27 | 1.9 | 13 | 0.8
Increased alkaline phosphatase | 26 | 0.7 | 18 | 0.8
Increased ALT | 22 | 1.7 | 17 | 0.5
Increased creatinine | 18 | 0 | 12 | 0.5
Increased TSHb | 14 | N/A | 6 | N/A
a Each test incidence is based on the number of patients who had both baseline and at least one on-study laboratory measurement available: OPDIVO group (range: 405 to 417 patients) and docetaxel group (range: 372 to 390 patients), except for TSH: OPDIVO group n=314 and docetaxel group n=297.
b Not graded per NCI CTCAE v4.

Malignant Pleural Mesothelioma

The safety of OPDIVO in combination with ipilimumab was evaluated in CHECKMATE-743, a randomized, open-label trial in patients with previously untreated unresectable malignant pleural mesothelioma [see Clinical Studies (14.6)]. Patients received either OPDIVO 3 mg/kg over 30 minutes by intravenous infusion every 2 weeks and ipilimumab 1 mg/kg over 30 minutes by intravenous infusion every 6 weeks for up to 2 years; or platinum-doublet chemotherapy for up to 6 cycles. The median duration of therapy in OPDIVO and ipilimumab-treated patients was 5.6 months (range: 0 to 26.2 months); 48% of patients received OPDIVO and ipilimumab for >6 months and 24% of patients received OPDIVO and ipilimumab for >1 year.

Serious adverse reactions occurred in 54% of patients who were treated with OPDIVO in combination with ipilimumab. The most frequent (≥2%) serious adverse reactions were pneumonia, pyrexia, diarrhea, pneumonitis, pleural effusion, dyspnea, acute kidney injury, infusion-related reaction, musculoskeletal pain, and pulmonary embolism. Fatal adverse reactions occurred in 4 (1.3%) patients and included pneumonitis, acute heart failure, sepsis and encephalitis.

Both OPDIVO and ipilimumab were permanently discontinued due to adverse reactions in 23% of patients and 52% had at least one dose withheld due to an adverse reaction.

The most common (≥20%) adverse reactions were fatigue, musculoskeletal pain, rash, diarrhea, dyspnea, nausea, decreased appetite, cough, and pruritus.

Tables 23 and 24 summarize adverse reactions and laboratory abnormalities, respectively, in CHECKMATE-743.

Table 23: Adverse Reactions in ≥10% of Patients Receiving OPDIVO and Ipilimumab - CHECKMATE-743
Adverse Reaction | OPDIVO and Ipilimumab (n=300) |  | Chemotherapy (n=284)
Adverse Reaction | All Grades (%) | Grades 3-4 (%) | All Grades (%) | Grades 3-4 (%)
General
Fatiguea | 43 | 4.3 | 45 | 6
Pyrexiab | 18 | 1.3 | 4.6 | 0.7
Edemac | 17 | 0 | 8 | 0
Musculoskeletal and Connective Tissue
Musculoskeletal paind | 38 | 3.3 | 17 | 1.1
Arthralgia | 13 | 1 | 1.1 | 0
Skin and Subcutaneous Tissue
Rashe | 34 | 2.7 | 11 | 0.4
Pruritusf | 21 | 1 | 1.4 | 0
Gastrointestinal
Diarrheag | 32 | 6 | 12 | 1.1
Nausea | 24 | 0.7 | 43 | 2.5
Constipation | 19 | 0.3 | 30 | 0.7
Abdominal painh | 15 | 1 | 10 | 0.7
Vomiting | 14 | 0 | 18 | 2.1
Respiratory, Thoracic, and Mediastinal
Dyspneai | 27 | 2.3 | 16 | 3.2
Coughj | 23 | 0.7 | 9 | 0
Metabolism and Nutrition
Decreased appetite | 24 | 1 | 25 | 1.4
Endocrine
Hypothyroidismk | 15 | 0 | 1.4 | 0
Infections and Infestations
Upper respiratory tract infectionl | 12 | 0.3 | 7 | 0
Pneumoniam | 10 | 4 | 4.2 | 2.1
a Includes fatigue and asthenia.
b Includes pyrexia and tumor-associated fever.
c Includes edema, generalized edema, peripheral edema, and peripheral swelling.
d Includes musculoskeletal pain, back pain, bone pain, flank pain, involuntary muscle contractions, muscle spasms, muscle twitching, musculoskeletal chest pain, musculoskeletal stiffness, myalgia, neck pain, non-cardiac chest pain, pain in extremity, polymyalgia rheumatica, and spinal pain.
e Includes rash, acne, acneiform dermatitis, allergic dermatitis, atopic dermatitis, autoimmune dermatitis, bullous dermatitis, contact dermatitis, dermatitis, drug eruption, dyshidrotic eczema, eczema, erythematous rash, exfoliative rash, generalized exfoliative dermatitis, generalized rash, granulomatous dermatitis, keratoderma blennorrhagica, macular rash, maculopapular rash, morbilliform rash, nodular rash, papular rash, psoriasiform dermatitis, pruritic rash, pustular rash, skin exfoliation, skin reaction, skin toxicity, Stevens-Johnson syndrome, toxic skin eruption, and urticaria.
f Includes pruritus, allergic pruritus, and generalized pruritus.
g Includes diarrhea, colitis, enteritis, infectious enteritis, enterocolitis, infectious enterocolitis, microscopic colitis, ulcerative colitis, and viral enterocolitis.
h Includes abdominal pain, abdominal discomfort, abdominal tenderness, gastrointestinal pain, lower abdominal pain, and upper abdominal pain.
i Includes dyspnea, dyspnea at rest, and exertional dyspnea.
j Includes cough, productive cough, and upper-airway cough syndrome.
k Includes hypothyroidism, autoimmune thyroiditis, decreased free tri-iodothyronine, increased blood thyroid stimulating hormone, primary hypothyroidism, thyroiditis, and autoimmune hypothyroidism.
l Includes upper respiratory tract infection, nasopharyngitis, pharyngitis, and rhinitis.
m Includes pneumonia, lower respiratory tract infection, lung infection, aspiration pneumonia, and Pneumocystis jirovecii pneumonia.

Table 24: Laboratory Values Worsening from Baselinea Occurring in ≥20% of Patients on OPDIVO and Ipilimumab - CHECKMATE-743
Laboratory Abnormality | OPDIVO and Ipilimumab |  | Chemotherapy
Laboratory Abnormality | Grades 1-4 (%) | Grades 3-4 (%) | Grades 1-4 (%) | Grades 3-4 (%)
Chemistry
Hyperglycemia | 53 | 3.7 | 34 | 1.1
Increased AST | 38 | 7 | 17 | 0
Increased ALT | 37 | 7 | 15 | 0.4
Increased lipase | 34 | 13 | 9 | 0.8
Hyponatremia | 32 | 8 | 21 | 2.9
Increased alkaline phosphatase | 31 | 3.1 | 12 | 0
Hyperkalemia | 30 | 4.1 | 16 | 0.7
Hypocalcemia | 28 | 0 | 16 | 0
Increased amylase | 26 | 5 | 13 | 0.9
Increased creatinine | 20 | 0.3 | 20 | 0.4
Hematology
Lymphopenia | 43 | 8 | 57 | 14
Anemia | 43 | 2.4 | 75 | 15
a Each test incidence is based on the number of patients who had both baseline and at least one on-study laboratory measurement available: OPDIVO and ipilimumab group (range: 109 to 297 patients) and chemotherapy group (range: 90 to 276 patients).

Advanced Renal Cell Carcinoma

First-line Renal Cell Carcinoma

CHECKMATE-214

The safety of OPDIVO with ipilimumab was evaluated in CHECKMATE-214, a randomized open-label trial in 1082 patients with previously untreated advanced RCC received OPDIVO 3 mg/kg over 60 minutes with ipilimumab 1 mg/kg intravenously every 3 weeks for 4 doses followed by OPDIVO as a single agent at a dose of 3 mg/kg by intravenous infusion every 2 weeks (n=547) or sunitinib 50 mg orally daily for the first 4 weeks of a 6-week cycle (n=535) [see Clinical Studies (14.7)]. The median duration of treatment was 7.9 months (range: 1 day to 21.4+ months) in OPDIVO and ipilimumab-treated patients and 7.8 months (range: 1 day to 20.2+ months) in sunitinib-treated patients. In this trial, 57% of patients in the OPDIVO and ipilimumab arm were exposed to treatment for >6 months and 38% of patients were exposed to treatment for >1 year.

Serious adverse reactions occurred in 59% of patients receiving OPDIVO and ipilimumab. Study therapy was discontinued for adverse reactions in 31% of OPDIVO and ipilimumab patients. Fifty-four percent (54%) of patients receiving OPDIVO and ipilimumab had a dose interruption for an adverse reaction.

The most frequent serious adverse reactions reported in ≥2% of patients treated with OPDIVO and ipilimumab were diarrhea, pyrexia, pneumonia, pneumonitis, hypophysitis, acute kidney injury, dyspnea, adrenal insufficiency, and colitis; in patients treated with sunitinib, they were pneumonia, pleural effusion, and dyspnea. The most common adverse reactions (reported in ≥20% of patients) were fatigue, rash, diarrhea, musculoskeletal pain, pruritus, nausea, cough, pyrexia, arthralgia, and decreased appetite. The most common laboratory abnormalities which have worsened compared to baseline in ≥30% of OPDIVO and ipilimumab-treated patients include increased lipase, anemia, increased creatinine, increased ALT, increased AST, hyponatremia, increased amylase, and lymphopenia.

Tables 25 and 26 summarize adverse reactions and laboratory abnormalities, respectively, that occurred in >15% of OPDIVO and ipilimumab-treated patients in CHECKMATE-214.

Table 25: Adverse Reactions in >15% of Patients Receiving OPDIVO and Ipilimumab - CHECKMATE-214
Adverse Reaction | OPDIVO and Ipilimumab (n=547) |  | Sunitinib (n=535)
Adverse Reaction | Grades 1-4 (%) | Grades 3-4 (%) | Grades 1-4 (%) | Grades 3-4 (%)
Adverse Reaction | 99 | 65 | 99 | 76
General
Fatiguea | 58 | 8 | 69 | 13
Pyrexia | 25 | 0.7 | 17 | 0.6
Edemab | 16 | 0.5 | 17 | 0.6
Skin and Subcutaneous Tissue
Rashc | 39 | 3.7 | 25 | 1.1
Pruritus/generalized pruritus | 33 | 0.5 | 11 | 0
Gastrointestinal
Diarrhea | 38 | 4.6 | 58 | 6
Nausea | 30 | 2 | 43 | 1.5
Vomiting | 20 | 0.9 | 28 | 2.1
Abdominal pain | 19 | 1.6 | 24 | 1.9
Constipation | 17 | 0.4 | 18 | 0
Musculoskeletal and Connective Tissue
Musculoskeletal paind | 37 | 4 | 40 | 2.6
Arthralgia | 23 | 1.3 | 16 | 0
Respiratory, Thoracic and Mediastinal
Cough/productive cough | 28 | 0.2 | 25 | 0.4
Dyspnea/exertional dyspnea | 20 | 2.4 | 21 | 2.1
Metabolism and Nutrition
Decreased appetite | 21 | 1.8 | 29 | 0.9
Nervous System
Headache | 19 | 0.9 | 23 | 0.9
Endocrine
Hypothyroidism | 18 | 0.4 | 27 | 0.2
Toxicity was graded per NCI CTCAE v4.
a Includes asthenia.
b Includes peripheral edema, peripheral swelling.
c Includes dermatitis described as acneiform, bullous, and exfoliative, drug eruption, rash described as exfoliative, erythematous, follicular, generalized, macular, maculopapular, papular, pruritic, and pustular, fixed-drug eruption.
d Includes back pain, bone pain, musculoskeletal chest pain, musculoskeletal discomfort, myalgia, neck pain, pain in extremity, spinal pain.

Table 26: Laboratory Values Worsening from Baselinea Occurring in >15% of Patients on OPDIVO and Ipilimumab - CHECKMATE-214
Laboratory Abnormality | OPDIVO and Ipilimumab |  | Sunitinib
Laboratory Abnormality | Grades 1-4 (%) | Grades 3-4 (%) | Grades 1-4 (%) | Grades 3-4 (%)
Chemistry
Increased lipase | 48 | 20 | 51 | 20
Increased creatinine | 42 | 2.1 | 46 | 1.7
Increased ALT | 41 | 7 | 44 | 2.7
Increased AST | 40 | 4.8 | 60 | 2.1
Increased amylase | 39 | 12 | 33 | 7
Hyponatremia | 39 | 10 | 36 | 7
Increased alkaline phosphatase | 29 | 2 | 32 | 1
Hyperkalemia | 29 | 2.4 | 28 | 2.9
Hypocalcemia | 21 | 0.4 | 35 | 0.6
Hypomagnesemia | 16 | 0.4 | 26 | 1.6
Hematology
Anemia | 43 | 3 | 64 | 9
Lymphopenia | 36 | 5 | 63 | 14
a Each test incidence is based on the number of patients who had both baseline and at least one on-study laboratory measurement available: OPDIVO and ipilimumab group (range: 490 to 538 patients) and sunitinib group (range: 485 to 523 patients).

In addition, among patients with TSH ≤ULN at baseline, a lower proportion of patients experienced a treatment-emergent elevation of TSH > ULN in the OPDIVO and ipilimumab group compared to the sunitinib group (31% and 61%, respectively).

CHECKMATE-9ER

The safety of OPDIVO with cabozantinib was evaluated in CHECKMATE-9ER, a randomized, open-label study in patients with previously untreated advanced RCC. Patients received OPDIVO 240 mg over 30 minutes every 2 weeks with cabozantinib 40 mg orally once daily (n=320) or sunitinib 50 mg daily, administered orally for 4 weeks on treatment followed by 2 weeks off (n=320) [see Clinical Studies (14.7)]. Cabozantinib could be interrupted or reduced to 20 mg daily or 20 mg every other day. The median duration of treatment was 14 months (range: 0.2 to 27 months) in OPDIVO and cabozantinib-treated patients. In this trial, 82% of patients in the OPDIVO and cabozantinib arm were exposed to treatment for >6 months and 60% of patients were exposed to treatment for >1 year.

Serious adverse reactions occurred in 48% of patients receiving OPDIVO and cabozantinib. The most frequent (≥2%) serious adverse reactions were diarrhea, pneumonia, pneumonitis, pulmonary embolism, urinary tract infection, and hyponatremia. Fatal intestinal perforations occurred in 3 (0.9%) patients.

Adverse reactions leading to discontinuation of either OPDIVO or cabozantinib occurred in 20% of patients: 7% OPDIVO only, 8% cabozantinib only, and 6% both drugs due to same adverse reaction at the same time. Adverse reaction leading to dose interruption or reduction of either OPDIVO or cabozantinib occurred in 83% of patients: 3% OPDIVO only, 46% cabozantinib only, and 21% both drugs due to same adverse reaction at the same time, and 6% both drugs sequentially.

The most common adverse reactions reported in ≥20% of patients treated with OPDIVO and cabozantinib were diarrhea, fatigue, hepatotoxicity, palmar-plantar erythrodysesthesia syndrome, stomatitis, rash, hypertension, hypothyroidism, musculoskeletal pain, decreased appetite, nausea, dysgeusia, abdominal pain, cough, and upper respiratory tract infection.

Tables 27 and 28 summarize adverse reactions and laboratory abnormalities, respectively, in CHECKMATE-9ER.

Table 27: Adverse Reactions in >15% of Patients Receiving OPDIVO and Cabozantinib - CHECKMATE-9ER
Adverse Reaction | OPDIVO and Cabozantinib (n=320) |  | Sunitinib (n=320)
Adverse Reaction | Grades 1-4 (%) | Grades 3-4 (%) | Grades 1-4 (%) | Grades 3-4 (%)
Gastrointestinal
Diarrhea | 64 | 7 | 47 | 4.4
Nausea | 27 | 0.6 | 31 | 0.3
Abdominal paina | 22 | 1.9 | 15 | 0.3
Vomiting | 17 | 1.9 | 21 | 0.3
Dyspepsiab | 15 | 0 | 22 | 0.3
General
Fatiguec | 51 | 8 | 50 | 8
Hepatobiliary
Hepatotoxicityd | 44 | 11 | 26 | 5
Skin and Subcutaneous Tissue
Palmar-plantar erythrodysesthesia syndrome | 40 | 8 | 41 | 8
Stomatitise | 37 | 3.4 | 46 | 4.4
Rashf | 36 | 3.1 | 14 | 0
Pruritus | 19 | 0.3 | 4.4 | 0
Vascular
Hypertensiong | 36 | 13 | 39 | 14
Endocrine
Hypothyroidismh | 34 | 0.3 | 30 | 0.3
Musculoskeletal and Connective Tissue
Musculoskeletal paini | 33 | 3.8 | 29 | 3.1
Arthralgia | 18 | 0.3 | 9 | 0.3
Metabolism and Nutrition
Decreased appetite | 28 | 1.9 | 20 | 1.3
Nervous System
Dysgeusia | 24 | 0 | 22 | 0
Headache | 16 | 0 | 12 | 0.6
Respiratory, Thoracic and Mediastinal
Coughj | 20 | 0.3 | 17 | 0
Dysphonia | 17 | 0.3 | 3.4 | 0
Infections and Infestations
Upper respiratory tract infectionk | 20 | 0.3 | 8 | 0.3
Toxicity was graded per NCI CTCAE v4.
a Includes abdominal discomfort, abdominal pain lower, abdominal pain upper.
b Includes gastroesophageal reflux disease.
c Includes asthenia.
d Includes hepatotoxicity, ALT increased, AST increased, blood alkaline phosphatase increased, gamma-glutamyl transferase increased, autoimmune hepatitis, blood bilirubin increased, drug induced liver injury, hepatic enzyme increased, hepatitis, hyperbilirubinemia, liver function test increased, liver function test abnormal, transaminases increased, hepatic failure.
e Includes mucosal inflammation, aphthous ulcer, mouth ulceration.
f Includes dermatitis, dermatitis acneiform, dermatitis bullous, exfoliative rash, rash erythematous, rash follicular, rash macular, rash maculo-papular, rash papular, rash pruritic.
g Includes blood pressure increased, blood pressure systolic increased.
h Includes primary hypothyroidism.
i Includes back pain, bone pain, musculoskeletal chest pain, musculoskeletal discomfort, myalgia, neck pain, pain in extremity, spinal pain.
j Includes productive cough.
k Includes nasopharyngitis, pharyngitis, rhinitis.

Table 28: Laboratory Values Worsening from Baselinea Occurring in >20% of Patients on OPDIVO and Cabozantinib - CHECKMATE-9ER
Laboratory Abnormality | OPDIVO and Cabozantinib |  | Sunitinib
Laboratory Abnormality | Grades 1-4 (%) | Grades 3-4 (%) | Grades 1-4 (%) | Grades 3-4 (%)
Chemistry
Increased ALT | 79 | 9.8 | 39 | 3.5
Increased AST | 77 | 7.9 | 57 | 2.6
Hypophosphatemia | 69 | 28 | 48 | 10
Hypocalcemia | 54 | 1.9 | 24 | 0.6
Hypomagnesemia | 47 | 1.3 | 25 | 0.3
Hyperglycemia | 44 | 3.5 | 44 | 1.7
Hyponatremia | 43 | 11 | 36 | 12
Increased lipase | 41 | 14 | 38 | 13
Increased amylase | 41 | 10 | 28 | 6
Increased alkaline phosphatase | 41 | 2.8 | 37 | 1.6
Increased creatinine | 39 | 1.3 | 42 | 0.6
Hyperkalemia | 35 | 4.7 | 27 | 1
Hypoglycemia | 26 | 0.8 | 14 | 0.4
Hematology
Lymphopenia | 42 | 6.6 | 45 | 10
Thrombocytopenia | 41 | 0.3 | 70 | 9.7
Anemia | 37 | 2.5 | 61 | 4.8
Leukopenia | 37 | 0.3 | 66 | 5.1
Neutropenia | 35 | 3.2 | 67 | 12
a Each test incidence is based on the number of patients who had both baseline and at least one on-study laboratory measurement available: OPDIVO and cabozantinib group (range: 170 to 317 patients) and sunitinib group (range: 173 to 311 patients).

Previously Treated Renal Cell Carcinoma

CHECKMATE-025

The safety of OPDIVO was evaluated in CHECKMATE-025, a randomized open-label trial in 803 patients with advanced RCC who had experienced disease progression during or after at least one anti-angiogenic treatment regimen received OPDIVO 3 mg/kg over 60 minutes by intravenous infusion every 2 weeks (n=406) or everolimus 10 mg daily (n=397) [see Clinical Studies (14.7)]. The median duration of treatment was 5.5 months (range: 1 day to 29.6+ months) in OPDIVO-treated patients and 3.7 months (range: 6 days to 25.7+ months) in everolimus-treated patients.

Rate of death on treatment or within 30 days of the last dose was 4.7% on the OPDIVO arm. Serious adverse reactions occurred in 47% of patients receiving OPDIVO. Study therapy was discontinued for adverse reactions in 16% of OPDIVO patients. Forty-four percent (44%) of patients receiving OPDIVO had a dose interruption for an adverse reaction.

The most frequent serious adverse reactions in at least 2% of patients were: acute kidney injury, pleural effusion, pneumonia, diarrhea, and hypercalcemia. The most common adverse reactions (≥20%) were fatigue, cough, nausea, rash, dyspnea, diarrhea, constipation, decreased appetite, back pain, and arthralgia. The most common laboratory abnormalities which have worsened compared to baseline in ≥30% of patients include increased creatinine, lymphopenia, anemia, increased AST, increased alkaline phosphatase, hyponatremia, increased triglycerides, and hyperkalemia. In addition, among patients with TSH < ULN at baseline, a greater proportion of patients experienced a treatment-emergent elevation of TSH >ULN in the OPDIVO group compared to the everolimus group (26% and 14%, respectively).

Tables 29 and 30 summarize adverse reactions and laboratory abnormalities, respectively, in CHECKMATE-025.

Table 29: Adverse Reactions in >15% of Patients Receiving OPDIVO - CHECKMATE-025
Adverse Reaction | OPDIVO (n=406) |  | Everolimus (n=397)
Adverse Reaction | Grades 1-4 (%) | Grades 3-4 (%) | Grades 1-4 (%) | Grades 3-4 (%)
Adverse Reaction | 98 | 56 | 96 | 62
General
Fatiguea | 56 | 6 | 57 | 7
Pyrexia | 17 | 0.7 | 20 | 0.8
Respiratory, Thoracic and Mediastinal
Cough/productive cough | 34 | 0 | 38 | 0.5
Dyspnea/exertional dyspnea | 27 | 3 | 31 | 2
Upper respiratory infectionb | 18 | 0 | 11 | 0
Gastrointestinal
Nausea | 28 | 0.5 | 29 | 1
Diarrheac | 25 | 2.2 | 32 | 1.8
Constipation | 23 | 0.5 | 18 | 0.5
Vomiting | 16 | 0.5 | 16 | 0.5
Skin and Subcutaneous Tissue
Rashd | 28 | 1.5 | 36 | 1
Pruritus/generalized pruritus | 19 | 0 | 14 | 0
Metabolism and Nutrition
Decreased appetite | 23 | 1.2 | 30 | 1.5
Musculoskeletal and Connective Tissue
Arthralgia | 20 | 1 | 14 | 0.5
Back pain | 21 | 3.4 | 16 | 2.8
Toxicity was graded per NCI CTCAE v4.
a Includes asthenia, decreased activity, fatigue, and malaise.
b Includes nasopharyngitis, pharyngitis, rhinitis, and viral upper respiratory infection (URI).
c Includes colitis, enterocolitis, and gastroenteritis.
d Includes dermatitis, acneiform dermatitis, erythematous rash, generalized rash, macular rash, maculopapular rash, papular rash, pruritic rash, erythema multiforme, and erythema.

Other clinically important adverse reactions in CHECKMATE-025 were:

General Disorders and Administration Site Conditions: peripheral edema/edema

Gastrointestinal Disorders: abdominal pain/discomfort

Musculoskeletal and Connective Tissue Disorders: extremity pain, musculoskeletal pain

Nervous System Disorders: headache/migraine, peripheral neuropathy

Investigations: weight decreased

Skin Disorders: palmar-plantar erythrodysesthesia

Table 30: Laboratory Values Worsening from Baselinea Occurring in >15% of Patients on OPDIVO - CHECKMATE-025
Laboratory Abnormality | OPDIVO |  | Everolimus
Laboratory Abnormality | Grades 1-4 (%) | Grades 3-4 (%) | Grades 1-4 (%) | Grades 3-4 (%)
Hematology
Lymphopenia | 42 | 6 | 53 | 11
Anemia | 39 | 8 | 69 | 16
Chemistry
Increased creatinine | 42 | 2 | 45 | 1.6
Increased AST | 33 | 2.8 | 39 | 1.6
Increased alkaline phosphatase | 32 | 2.3 | 32 | 0.8
Hyponatremia | 32 | 7 | 26 | 6
Hyperkalemia | 30 | 4 | 20 | 2.1
Hypocalcemia | 23 | 0.9 | 26 | 1.3
Increased ALT | 22 | 3.2 | 31 | 0.8
Hypercalcemia | 19 | 3.2 | 6 | 0.3
Lipids
Increased triglycerides | 32 | 1.5 | 67 | 11
Increased cholesterol | 21 | 0.3 | 55 | 1.4
a Each test incidence is based on the number of patients who had both baseline and at least one on-study laboratory measurement available: OPDIVO group (range: 259 to 401 patients) and everolimus group (range: 257 to 376 patients).

Classical Hodgkin Lymphoma

The safety of OPDIVO was evaluated in 266 adult patients with cHL (243 patients in the CHECKMATE-205 and 23 patients in the CHECKMATE-039 trials) [see Clinical Studies (14.8)]. Patients received OPDIVO 3 mg/kg as an intravenous infusion over 60 minutes every 2 weeks until disease progression, maximal clinical benefit, or unacceptable toxicity.

The median age was 34 years (range: 18 to 72), 98% of patients had received autologous HSCT, none had received allogeneic HSCT, and 74% had received brentuximab vedotin. The median number of prior systemic regimens was 4 (range: 2 to 15). Patients received a median of 23 doses (cycles) of OPDIVO (range: 1 to 48), with a median duration of therapy of 11 months (range: 0 to 23 months).

Eleven patients died from causes other than disease progression: 3 from adverse reactions within 30 days of the last nivolumab dose, 2 from infection 8 to 9 months after completing nivolumab, and 6 from complications of allogeneic HSCT. Serious adverse reactions occurred in 26% of patients. Dose delay for an adverse reaction occurred in 34% of patients. OPDIVO was discontinued due to adverse reactions in 7% of patients.

The most frequent serious adverse reactions reported in ≥1% of patients were pneumonia, infusion-related reaction, pyrexia, colitis or diarrhea, pleural effusion, pneumonitis, and rash. The most common adverse reactions (≥20%) among all patients were upper respiratory tract infection, fatigue, cough, diarrhea, pyrexia, musculoskeletal pain, rash, nausea, and pruritus.

Tables 31 and 32 summarize the adverse reactions and laboratory abnormalities, respectively, in CHECKMATE-205 and CHECKMATE-039.

Table 31: Adverse Reactions Occurring in ≥10% of Patients - CHECKMATE-205 and CHECKMATE-039
Adverse Reactiona | OPDIVO (n=266)
Adverse Reactiona | All Grades (%) | Grades 3-4 (%)
Infections
Upper respiratory tract infectionb | 44 | 0.8
Pneumonia/bronchopneumoniac | 13 | 3.8
Nasal congestion | 11 | 0
General
Fatigued | 39 | 1.9
Pyrexia | 29 | <1
Respiratory, Thoracic and Mediastinal
Cough/productive cough | 36 | 0
Dyspnea/exertional dyspnea | 15 | 1.5
Gastrointestinal
Diarrheae | 33 | 1.5
Nausea | 20 | 0
Vomiting | 19 | <1
Abdominal painf | 16 | <1
Constipation | 14 | 0.4
Musculoskeletal and Connective Tissue
Musculoskeletal paing | 26 | 1.1
Arthralgia | 16 | <1
Skin and Subcutaneous Tissue
Rashh | 24 | 1.5
Pruritus | 20 | 0
Nervous System
Headache | 17 | <1
Neuropathy peripherali | 12 | <1
Injury, Poisoning and Procedural Complications
Infusion-related reaction | 14 | <1
Endocrine
Hypothyroidism/thyroiditis | 12 | 0
Toxicity was graded per NCI CTCAE v4.
a Includes events occurring up to 30 days after last nivolumab dose, regardless of causality. After an immune-mediated adverse reaction, reactions following nivolumab rechallenge were included if they occurred up to 30 days after completing the initial nivolumab course.
b Includes nasopharyngitis, pharyngitis, rhinitis, and sinusitis.
c Includes pneumonia bacterial, pneumonia mycoplasmal, pneumocystis jirovecii pneumonia.
d Includes asthenia.
e Includes colitis.
f Includes abdominal discomfort and upper abdominal pain.
g Includes back pain, bone pain, musculoskeletal chest pain, musculoskeletal discomfort, myalgia, neck pain, and pain in extremity.
h Includes dermatitis, dermatitis acneiform, dermatitis exfoliative, and rash described as macular, papular, maculopapular, pruritic, exfoliative, or acneiform.
i Includes hyperesthesia, hypoesthesia, paresthesia, dysesthesia, peripheral motor neuropathy, peripheral sensory neuropathy, and polyneuropathy.
These numbers are specific to treatment-emergent events.

Additional information regarding clinically important adverse reactions:

Immune-mediated pneumonitis: In CHECKMATE-205 and CHECKMATE-039, pneumonitis, including interstitial lung disease, occurred in 6.0% (16/266) of patients receiving OPDIVO. Immune-mediated pneumonitis occurred in 4.9% (13/266) of patients receiving OPDIVO (one Grade 3 and 12 Grade 2). The median time to onset was 4.5 months (range: 5 days to 12 months). All 13 patients received systemic corticosteroids, with resolution in 12. Four patients permanently discontinued OPDIVO due to pneumonitis. Eight patients continued OPDIVO (three after dose delay), of whom two had recurrence of pneumonitis.

Peripheral neuropathy: Treatment-emergent peripheral neuropathy was reported in 12% (31/266) of all patients receiving OPDIVO. Twenty-eight patients (11%) had new-onset peripheral neuropathy and 3 patients had worsening of neuropathy from baseline. The median time to onset was 50 (range: 1 to 309) days.

Complications of allogeneic HSCT after OPDIVO: Of 17 patients with cHL from the CHECKMATE-205 and CHECKMATE-039 trials who underwent allogeneic HSCT after treatment with OPDIVO, 6 patients (35%) died from transplant-related complications. Five deaths occurred in the setting of severe (Grade 3 to 4) or refractory GVHD. Hyperacute GVHD occurred in 2 patients (12%) and Grade 3 or higher GVHD was reported in 5 patients (29%). Hepatic VOD occurred in 1 patient, who received reduced-intensity conditioned allogeneic HSCT and died of GVHD and multi-organ failure.

Table 32 summarizes laboratory abnormalities in patients with cHL. The most common (≥20%) treatment-emergent laboratory abnormalities included cytopenias, liver function abnormalities, and increased lipase. Other common findings (≥10%) included increased creatinine, electrolyte abnormalities, and increased amylase.

Table 32: Laboratory Abnormalities Worsening from Baselinea Occurring in ≥10% of Patients - CHECKMATE-205 and CHECKMATE-039
Laboratory Abnormality | OPDIVOa (n=266)
Laboratory Abnormality | All Grades (%)b | Grades 3-4 (%)b
Hematology
Leukopenia | 38 | 4.5
Neutropenia | 37 | 5
Thrombocytopenia | 37 | 3
Lymphopenia | 32 | 11
Anemia | 26 | 2.6
Chemistryc
Increased AST | 33 | 2.6
Increased ALT | 31 | 3.4
Increased lipase | 22 | 9
Increased alkaline phosphatase | 20 | 1.5
Hyponatremia | 20 | 1.1
Hypokalemia | 16 | 1.9
Increased creatinine | 16 | <1
Hypocalcemia | 15 | <1
Hyperkalemia | 15 | 1.5
Hypomagnesemia | 14 | <1
Increased amylase | 13 | 1.5
Increased bilirubin | 11 | 1.5
a Each test incidence is based on the number of patients who had both baseline and at least one on-study laboratory measurement: range: 203 to 266 patients.
b Includes events occurring up to 30 days after last nivolumab dose. After an immune-mediated adverse reaction, reactions following nivolumab rechallenge were included if they occurred within 30 days of completing the initial nivolumab course.
c In addition, in the safety population, fasting hyperglycemia (all grade 1-2) was reported in 27 of 69 (39%) evaluable patients and fasting hypoglycemia (all grade 1-2) in 11 of 69 (16%).

Squamous Cell Carcinoma of the Head and Neck

The safety of OPDIVO was evaluated in CHECKMATE-141, a randomized, active-controlled, open-label, multicenter trial in patients with recurrent or metastatic SCCHN with progression during or within 6 months of receiving prior platinum-based therapy [see Clinical Studies (14.9)]. The trial excluded patients with active autoimmune disease, medical conditions requiring systemic immunosuppression, or recurrent or metastatic carcinoma of the nasopharynx, squamous cell carcinoma of unknown primary histology, salivary gland or non-squamous histologies (e.g., mucosal melanoma). Patients received OPDIVO 3 mg/kg by intravenous infusion over 60 minutes every 2 weeks (n=236) or investigator’s choice of either cetuximab (400 mg/m^2 initial dose intravenously followed by 250 mg/m^2 weekly), or methotrexate (40 to 60 mg/m^2 intravenously weekly), or docetaxel (30 to 40 mg/m^2 intravenously weekly). The median duration of exposure to nivolumab was 1.9 months (range: 1 day to 16.1+ months) in OPDIVO-treated patients. In this trial, 18% of patients received OPDIVO for >6 months and 2.5% of patients received OPDIVO for >1 year.

The median age of all randomized patients was 60 years (range: 28 to 83); 28% of patients in the OPDIVO group were ≥65 years of age and 37% in the comparator group were ≥65 years of age, 83% were male and 83% were White, 12% were Asian, and 4% were Black. Baseline ECOG performance status was 0 (20%) or 1 (78%), 45% of patients received only one prior line of systemic therapy, the remaining 55% of patients had two or more prior lines of therapy, and 90% had prior radiation therapy.

Serious adverse reactions occurred in 49% of patients receiving OPDIVO. OPDIVO was discontinued in 14% of patients and was delayed in 24% of patients for an adverse reaction. Adverse reactions and laboratory abnormalities occurring in patients with SCCHN were generally similar to those occurring in patients with melanoma and NSCLC.

The most frequent serious adverse reactions reported in ≥2% of patients receiving OPDIVO were pneumonia, dyspnea, respiratory failure, respiratory tract infection, and sepsis. The most common adverse reactions occurring in ≥10% of OPDIVO-treated patients and at a higher incidence than investigator’s choice were cough and dyspnea. The most common laboratory abnormalities occurring in ≥10% of OPDIVO-treated patients and at a higher incidence than investigator’s choice were increased alkaline phosphatase, increased amylase, hypercalcemia, hyperkalemia, and increased TSH.

Adjuvant Treatment of Urothelial Carcinoma (UC)

The safety of OPDIVO was evaluated in CHECKMATE-274, a randomized, double-blind, multicenter trial of adjuvant OPDIVO versus placebo in adult patients who had undergone radical resection of UC originating in the bladder or upper urinary tract (renal pelvis or ureter) and were at high risk of recurrence [see Clinical Studies (14.10)]. Patients received OPDIVO 240 mg by intravenous infusion over 30 minutes every 2 weeks (n=351) or placebo (n=348) until recurrence or unacceptable toxicity for a maximum of 1 year. The median duration of OPDIVO treatment was 8.8 months (range: 0 to 12.5).

Serious adverse reactions occurred in 30% of OPDIVO patients. The most frequent serious adverse reaction reported in ≥2% of patients was urinary tract infection. Fatal adverse reactions occurred in 1% of patients; these included events of pneumonitis (0.6%). OPDIVO was discontinued for adverse reactions in 18% of patients. OPDIVO was delayed for adverse reaction in 33% of patients.

The most common adverse reactions (reported in ≥20% of patients) were rash, fatigue, diarrhea, pruritus, musculoskeletal pain, and urinary tract infection.

Tables 33 and 34 summarize adverse reactions and laboratory abnormalities, respectively, in CHECKMATE-274.

Table 33: Adverse Reactions Occurring in ≥10% of Patients - CHECKMATE-274
Adverse Reaction | OPDIVO; (n=351) |  | Placebo; (n=348)
Adverse Reaction | All Grades (%) | Grades 3-4 (%) | All Grades (%) | Grades 3-4 (%)
Skin and Subcutaneous Tissue
Rasha | 36 | 1.7 | 19 | 0.3
Pruritus | 30 | 0 | 16 | 0
General
Fatigue/Asthenia | 36 | 1.1 | 32 | 0.3
Pyrexia | 10 | 0.3 | 10 | 0.3
Gastrointestinal
Diarrheab | 30 | 2.8 | 27 | 1.7
Nausea | 16 | 0.6 | 13 | 0
Abdominal painc | 15 | 0.9 | 15 | 0.6
Constipation | 13 | 0.3 | 15 | 0.3
Musculoskeletal and Connective Tissue
Musculoskeletal paind | 28 | 0.6 | 24 | 0.9
Arthralgia | 11 | 0.3 | 13 | 0
Infections
Urinary tract infectione | 22 | 6 | 23 | 9
Upper respiratory tract infectionf | 16 | 0.3 | 16 | 0.6
Endocrine
Hyperthyroidism | 11 | 0 | 1.1 | 0
Hypothyroidism | 11 | 0 | 2.3 | 0
Renal and Urinary Disorders
Renal dysfunctiong | 17 | 1.7 | 16 | 0.9
Respiratory, Thoracic and Mediastinal
Coughh | 14 | 0 | 11 | 0
Dyspneai | 11 | 0.3 | 6 | 0.3
Metabolism and Nutrition
Decreased appetite | 13 | 0.9 | 7 | 0.3
Nervous System Disorders
Dizzinessj | 11 | 0.3 | 9 | 0
Hepatobiliary
Hepatitisk | 11 | 4 | 8 | 0.6
Toxicity was graded per NCI CTCAE v4.
a Includes acne, blister, dermatitis, dermatitis acneiform, dermatitis allergic, dermatitis contact, eczema, eczema asteatotic, eczema nummular, erythema, erythema multiforme, lichen sclerosus, lichenoid keratosis, pemphigoid, photosensitivity reaction, pigmentation disorder, psoriasis, rash, rash erythematous, rash macular, rash maculo-papular, rash papular, rash pruritic, rosacea, skin exfoliation, skin lesion, skin reaction, toxic skin eruption, and urticaria.
b Includes colitis, colitis microscopic, diarrhea, duodenitis, enteritis, immune-mediated enterocolitis.
c Includes abdominal pain, abdominal discomfort, abdominal tenderness, lower and upper abdominal pain.
d Includes musculoskeletal pain, back pain, bone pain, musculoskeletal chest pain, musculoskeletal discomfort, myalgia, neck pain, pain in extremity and spinal pain.
e Includes cystitis, escherichia urinary tract infection, pyelonephritis, pyelonephritis acute, pyelonephritis chronic, urethritis, urinary tract infection, urinary tract infection bacterial, urinary tract infection staphylococcal, and urosepsis.
f Includes upper respiratory tract infection, nasopharyngitis, pharyngitis and rhinitis.
g Includes acute kidney injury, autoimmune nephritis, blood creatinine increased, glomerular filtration rate decreased, immune-mediated nephritis, nephritis, renal failure, and renal impairment.
h Includes cough, productive cough, and upper-airway cough syndrome.
i Includes dyspnea and exertional dyspnea.
j Includes dizziness, postural dizziness and vertigo.
k Includes aspartate aminotransferase increased, alanine aminotransferase increased, blood bilirubin increased, cholangitis, drug-induced liver injury, hepatic failure, hepatic function abnormal, hepatitis, hepatocellular injury, hyperbilirubinemia, gamma-glutamyl transferase increased, liver injury, and transaminases increased.

Table 34: Laboratory Abnormalities Worsening from Baselinea Occurring in ≥10% of Patients - CHECKMATE-274
Laboratory Abnormality | OPDIVO; (n=351) |  | Placebo; (n=348)
Laboratory Abnormality | All Grades (%) | Grades 3-4 (%) | All Grades (%) | Grades 3-4 (%)
Chemistry
Increased creatinine | 36 | 1.7 | 36 | 2.6
Increased amylase | 34 | 8 | 23 | 3.2
Increased lipase | 33 | 12 | 31 | 10
Hyperkalemia | 32 | 5 | 30 | 6
Increased alkaline phosphatase | 24 | 2.3 | 15 | 0.6
Increased AST | 24 | 3.5 | 16 | 0.9
Increased ALT | 23 | 2.9 | 15 | 0.6
Hyponatremia | 22 | 4.1 | 17 | 1.8
Hypocalcemia | 17 | 1.2 | 11 | 0.9
Hypomagnesemia | 16 | 0 | 9 | 0
Hypercalcemia | 12 | 0.3 | 8 | 0.3
Hematology
Lymphopenia | 33 | 2.9 | 27 | 1.5
Anemia | 30 | 1.4 | 28 | 0.9
Neutropenia | 11 | 0.6 | 10 | 0.3
a Each test incidence is based on the number of patients who had both baseline and at least one on-study laboratory measurement available: OPDIVO group (range: 322 to 348 patients) and placebo group (range: 312 to 341 patients).

First-line Treatment of Unresectable or Metastatic UC

The safety of OPDIVO was evaluated in CHECKMATE-901, a randomized, open-label trial in cisplatin-eligible patients with unresectable or metastatic UC [see Clinical Studies (14.10)]. Patients received either OPDIVO 360 mg with cisplatin and gemcitabine every 3 weeks for up to 6 cycles followed by single-agent OPDIVO 480 mg every 4 weeks up to 2 years (n=304), or cisplatin and gemcitabine chemotherapy every 3 weeks for up to 6 cycles (n=288). Patients discontinuing cisplatin alone were permitted to switch to carboplatin.

Among patients who received OPDIVO with chemotherapy, the median duration of OPDIVO exposure was 7.4 months (range: 0.03 to 47.9 months). Serious adverse reactions occurred in 48% of patients receiving OPDIVO in combination with chemotherapy. The most frequent serious adverse reactions reported in ≥2% of patients who received OPDIVO with chemotherapy were urinary tract infection (4.9%), acute kidney injury (4.3%), anemia (3%), pulmonary embolism (2.6%), sepsis (2.3%), and platelet count decreased (2.3%). The most common adverse reactions (reported in ≥20% of patients) were nausea, fatigue, musculoskeletal pain, constipation, decreased appetite, rash, vomiting, and peripheral neuropathy.

Fatal adverse reactions occurred in 3.6% of patients who received OPDIVO in combination with chemotherapy; these included sepsis (1%).

OPDIVO and/or chemotherapy were discontinued in 30% of patients and were delayed in 67% of patients for an adverse reaction.

Tables 35 and 36 summarize the adverse reactions and laboratory abnormalities, respectively, in CHECKMATE-901.

Table 35: Adverse Reactions Occurring in ≥10% of Treated Patients - CHECKMATE-901
Adverse Reaction | OPDIVO and Platinum-Doublet Chemotherapy (n=304) |  | Platinum-Doublet Chemotherapy (n=288)
Adverse Reaction | All Grades (%) | Grades 3-4 (%) | All Grades (%) | Grades 3-4 (%)
Gastrointestinal disorders
Nausea | 52 | 0.3 | 53 | 1
Constipation | 30 | 0 | 28 | 0.7
Vomiting | 23 | 1.3 | 19 | 2.1
Diarrheaa | 19 | 2 | 14 | 0
Abdominal painb | 14 | 0.3 | 9 | 0.3
General
Fatiguec | 48 | 3.9 | 43 | 4.2
Edemad | 18 | 0 | 9 | 0.3
Pyrexiae | 14 | 1 | 14 | 0
Musculoskeletal and Connective Tissue
Musculoskeletal painf | 33 | 3 | 21 | 0.3
Metabolism and Nutrition
Decreased appetite | 30 | 1.6 | 19 | 1
Skin and Subcutaneous Tissue
Rashg | 25 | 2.3 | 7 | 0.3
Pruritus | 17 | 0.7 | 3.5 | 0
Nervous System Disorders
Peripheral neuropathyh | 20 | 0.7 | 14 | 0
Headachei | 11 | 0 | 5 | 0
Infections
Urinary tract infectionj | 19 | 8 | 18 | 8
Endocrine disorders
Hypothyroidismk | 17 | 0 | 0.3 | 0
Renal and Urinary Disorders
Renal dysfunctionl | 14 | 6 | 11 | 1.7
Hematuria | 11 | 1 | 7 | 1.4
Investigations
Weight decreased | 11 | 0.3 | 6 | 0
Toxicity was graded per NCI CTCAE v4.
a Includes colitis, immune-mediated enterocolitis.
b Includes upper abdominal pain, lower abdominal pain, abdominal discomfort, epigastric discomfort, gastrointestinal pain, and hepatic pain.
c Includes asthenia.
d Includes peripheral edema, swelling, peripheral swelling, localized edema, swelling, face edema, testicular edema, gravitational edema, and edema genital.
e Includes hyperthermia, body temperature increased and hyperpyrexia.
f Includes back pain, arthralgia, bone pain, arthritis, musculoskeletal chest pain, non-cardiac chest pain, myalgia, neck pain, pain in extremity, and spinal pain.
g Includes maculopapular rash, erythematous rash, macular rash, papular rash, pustular rash, acneiform dermatitis, dermatitis, allergic dermatitis, atopic dermatitis, exfoliative rash, eczema asteatotic, erythema multiforme, palmar-plantar erythrodysesthesia syndrome, eczema, dermatitis exfoliative generalized, and skin exfoliation.
h Includes paresthesia, peripheral sensory neuropathy, hypoesthesia, dysesthesia, neuralgia, hyperesthesia, peripheral motor neuropathy, polyneuropathy.
i Includes occipital neuralgia.
j Includes urosepsis, cystitis, pyelonephritis, pyelonephritis acute, urinary tract infection enterococcal, escherichia urinary tract infection.
k Includes blood stimulating hormone increased.
l Includes acute kidney injury, renal failure, renal impairment, glomerular filtration rate decreased, anuria, azotemia.

Table 36: Selected Laboratory Abnormalities Worsening from Baselinea Occurring in ≥20% of Patients - CHECKMATE-901
Laboratory Abnormality | OPDIVO and Platinum-Doublet Chemotherapy (n=304) |  | Platinum-Doublet Chemotherapy (n=288)
Laboratory Abnormality | Grades 1-4 (%) | Grades 3-4 (%) | Grades 1-4 (%) | Grades 3-4 (%)
Hematology
Anemia | 88 | 21 | 80 | 21
Neutropenia | 82 | 35 | 76 | 28
Lymphopenia | 71 | 17 | 56 | 13
Thrombocytopenia | 60 | 13 | 51 | 8
Chemistry
Increased creatinine | 53 | 2.4 | 42 | 1.1
Hypomagnesemia | 48 | 3.8 | 39 | 1.5
Hyponatremia | 43 | 13 | 39 | 8
Hyperglycemia | 41 | 3.9 | 37 | 3.2
Hypocalcemia | 36 | 2.1 | 24 | 1.1
Hyperkalemia | 33 | 3.0 | 32 | 1.1
Increased amylase | 32 | 4.2 | 23 | 3.6
Increased AST | 31 | 2.4 | 17 | 0.7
Increased ALT | 29 | 2.4 | 19 | 0.7
a Each test incidence is based on the number of patients who had both baseline and at least one on-study laboratory measurement available: OPDIVO group (range: 289-301 patients) and chemotherapy group (range: 265-281 patients).

Previously Treated Advanced or Metastatic UC

The safety of OPDIVO was evaluated in CHECKMATE-275, a single arm trial in which 270 patients with locally advanced or metastatic UC had disease progression during or following platinum-containing chemotherapy or had disease progression within 12 months of neoadjuvant or adjuvant treatment with platinum-containing chemotherapy [see Clinical Studies (14.10)]. Patients received OPDIVO 3 mg/kg by intravenous infusion over 60 minutes every 2 weeks until disease progression or unacceptable toxicity. The median duration of treatment was 3.3 months (range: 0 to 13.4+). Forty-six percent (46%) of patients had a dose interruption for an adverse reaction.

Fourteen patients (5.2%) died from causes other than disease progression. This includes 4 patients (1.5%) who died from pneumonitis or cardiovascular failure which was attributed to treatment with OPDIVO. Serious adverse reactions occurred in 54% of patients. OPDIVO was discontinued for adverse reactions in 17% of patients.

The most frequent serious adverse reactions reported in ≥2% of patients were urinary tract infection, sepsis, diarrhea, small intestine obstruction, and general physical health deterioration. The most common adverse reactions (reported in ≥20% of patients) were fatigue, musculoskeletal pain, nausea, and decreased appetite.

Tables 37 and 38 summarize adverse reactions and laboratory abnormalities, respectively, in CHECKMATE-275.

Table 37: Adverse Reactions Occurring in ≥10% of Patients - CHECKMATE-275
Adverse Reaction | OPDIVO (n=270)
Adverse Reaction | All Grades (%) | Grades 3-4 (%)
Adverse Reaction | 99 | 51
General
Asthenia/fatigue/malaise | 46 | 7
Pyrexia/tumor associated fever | 17 | 0.4
Edema/peripheral edema/peripheral swelling | 13 | 0.4
Musculoskeletal and Connective Tissue
Musculoskeletal paina | 30 | 2.6
Arthralgia | 10 | 0.7
Metabolism and Nutrition
Decreased appetite | 22 | 2.2
Gastrointestinal
Nausea | 22 | 0.7
Diarrhea | 17 | 2.6
Constipation | 16 | 0.4
Abdominal painb | 13 | 1.5
Vomiting | 12 | 1.9
Respiratory, Thoracic and Mediastinal
Cough/productive cough | 18 | 0
Dyspnea/exertional dyspnea | 14 | 3.3
Infections
Urinary tract infection/escherichia/fungal urinary tract infection | 17 | 7
Skin and Subcutaneous Tissue
Rashc | 16 | 1.5
Pruritus | 12 | 0
Endocrine
Thyroid disordersd | 15 | 0
Toxicity was graded per NCI CTCAE v4.
a Includes back pain, bone pain, musculoskeletal chest pain, musculoskeletal discomfort, myalgia, neck pain, pain in extremity and spinal pain.
b Includes abdominal discomfort, lower and upper abdominal pain.
c Includes dermatitis, dermatitis acneiform, dermatitis bullous, and rash described as generalized, macular, maculopapular, or pruritic.
d Includes autoimmune thyroiditis, blood TSH decrease, blood TSH increase, hyperthyroidism, hypothyroidism, thyroiditis, thyroxine decreased, thyroxine free increased, thyroxine increased, tri-iodothyronine free increased, tri-iodothyronine increased.

Table 38: Laboratory Abnormalities Worsening from Baseline Occurring in ≥10% of Patients - CHECKMATE-275
Laboratory Abnormality | OPDIVOa
Laboratory Abnormality | All Grades (%) | Grades 3-4 (%)
Chemistry
Hyperglycemia | 42 | 2.4
Hyponatremia | 41 | 11
Increased creatinine | 39 | 2
Increased alkaline phosphatase | 33 | 5.5
Hypocalcemia | 26 | 0.8
Increased AST | 24 | 3.5
Increased lipase | 20 | 7
Hyperkalemia | 19 | 1.2
Increased ALT | 18 | 1.2
Increased amylase | 18 | 4.4
Hypomagnesemia | 16 | 0
Hematology
Lymphopenia | 42 | 9
Anemia | 40 | 7
Thrombocytopenia | 15 | 2.4
Leukopenia | 11 | 0
a Each test incidence is based on the number of patients who had both baseline and at least one on-study laboratory measurement available: range: 84 to 256 patients.

MSI-H or dMMR Metastatic Colorectal Cancer

Treatment of MSI-H or dMMR mCRC: In Combination with Ipilimumab

The safety of OPDIVO in combination with ipilimumab, or as a single agent, was evaluated in CHECKMATE-8HW, a randomized, open-label, three arm trial in immunotherapy naive patients with MSI-H or dMMR mCRC [see Clinical Studies (14.11)]. Patients received one of the following:

- OPDIVO 240 mg every 3 weeks and ipilimumab 1 mg/kg every 3 weeks for a maximum of 4 doses, then OPDIVO 480 mg every 4 weeks.
- OPDIVO 240 mg every 2 weeks for 6 doses, then OPDIVO 480 mg every 4 weeks.
- Investigator’s choice chemotherapy: mFOLFOX or FOLFIRI [see Clinical Studies (14.11)].

In the OPDIVO and ipilimumab arm, the median duration of exposure to OPDIVO was 20.5 months (range: 0 to 35.9 months), 70% of patients were exposed for >6 months and 63% were exposed for >1 year. In the OPDIVO arm, the median duration of exposure to OPDIVO was 16.4 months (range: 0 to 36 months), 64% of patients were exposed for >6 months and 54% were exposed for >1 year.

Serious adverse reactions occurred in 46% of patients receiving OPDIVO in combination with ipilimumab, and 39% of patients receiving OPDIVO alone. The most frequent serious adverse reactions reported in ≥1% of patients who received OPDIVO with ipilimumab were adrenal insufficiency (2.8%), hypophysitis (2.8%), diarrhea (2.0%), abdominal pain (2.0%), small intestinal obstruction (2.0%), pneumonia (1.7%), acute kidney injury (1.4%), immune mediated enterocolitis (1.4%), pneumonitis (1.4%), colitis (1.1%), large intestinal obstruction (1.1%), and urinary tract infection (1.1%). The most frequent serious adverse reactions reported in >1% of patients who received OPDIVO, as a single agent, were intestinal obstruction (2.3%), acute kidney injury (1.7%), COVID-19 (1.7%), abdominal pain (1.4%), diarrhea (1.4%), ileus (1.4%), subileus (1.4%), pulmonary embolism (1.4%), adrenal insufficiency (1.1%) and pneumonia (1.1%).

Fatal adverse reactions occurred in 2 (0.6%) patients who received OPDIVO in combination with ipilimumab; these included myocarditis, and pneumonitis (1 each). Fatal adverse reactions occurring in 3 (0.9%) patients who received OPDIVO as a single agent; these included pneumonitis (n=2) and myasthenia gravis.

OPDIVO and/or ipilimumab were permanently discontinued in 19% of patients receiving the combination. The most frequent adverse reactions (>1%) leading to permanent discontinuation were adrenal insufficiency (1.4%), immune mediated enterocolitis (1.1%), and pneumonitis (1.1%). OPDIVO was permanently discontinued in 13% of patients receiving single agent OPDIVO. Adverse reactions leading to the delay of OPDIVO and/or ipilimumab occurred in 48% of patients receiving the combination; single agent OPDIVO was delayed in 37% of patients due to adverse reactions.

The most common adverse reactions reported in ≥20% of patients treated with OPDIVO in combination with ipilimumab were fatigue, diarrhea, pruritus, abdominal pain, musculoskeletal pain, and nausea. The most common adverse reactions reported in ≥20% of patients treated with OPDIVO as a single agent, were fatigue, diarrhea, abdominal pain, pruritus, and musculoskeletal pain.

Tables 39 and 40 summarize selected adverse reactions and selected laboratory abnormalities for OPDIVO in combination with ipilimumab and the single agent OPDIVO arms respectively, in CHECKMATE-8HW.

Table 39: Adverse Reactionsa in ≥10% in Patients with a Difference Between Arms of >5% for All Grades in CHECKMATE-8HW
Adverse Reaction | OPDIVO and ipilimumab (n=352) |  | OPDIVO (n=351)
Adverse Reaction | All Grades (%) | Grades 3 or 4 (%) | All Grades (%) | Grades 3 or4 (%)
Gastrointestinal
Diarrheaa | 35 | 4.5 | 30 | 3.4
Skin and Subcutaneous Tissue
Pruritus | 30 | 0 | 23 | 0
Musculoskeletal and Connective Tissue
Arthralgia | 20 | 0.6 | 15 | 0.6
Endocrine
Hypothyroidism | 18 | 0.6 | 10 | 0
Hyperthyroidism | 12 | 0 | 5 | 0
Toxicity was graded per NCI CTCAE v5.
a Includes colitis, diarrhea, enterocolitis, immune mediated enterocolitis

Table 40: Laboratory Values Worsening from Baselinea in ≥10% of Patients and a Difference Between Arms of >5% for All Grades - CHECKMATE-8HW
Laboratory Abnormalitya | OPDIVO and Ipilimumab (n=352) |  | OPDIVO (n=351)
Laboratory Abnormalitya | All Grades (%) | Grades 3-or 4 (%) | All Grades (%) | Grades 3 or -4 (%)
Hematology
Lymphocytes decreased | 30 | 5 | 37 | 4
Neutrophils decreased | 21 | 1.7 | 12 | 0.6
Chemistry
Lipase increased | 44 | 10 | 32 | 11
Amylase increased | 41 | 4.6 | 33 | 5
ALT increased | 39 | 3.5 | 32 | 1.4
AST increased | 38 | 3.2 | 29 | 1.4
Sodium decreased | 36 | 3.2 | 30 | 2.3
Creatinine increased | 32 | 2 | 25 | 1.4
Potassium increased | 29 | 1.2 | 35 | 0.9
Glucose decreased | 17 | 0 | 12 | 0
a Each test incidence is based on the number of patients who had both baseline and at least one on-study laboratory measurement available: OPDIVO and ipilimumab group (range: 108 to 343 patients) or nivolumab group (range: 102 to 348 patients).

MSI-H or dMMR mCRC After Progression Following Treatment with a Fluoropyrimidine, Oxaliplatin, and Irinotecan

The safety of OPDIVO administered as a single agent or in combination with ipilimumab was evaluated in CHECKMATE-142, a multicenter, non-randomized, multiple parallel-cohort, open-label trial [see Clinical Studies (14.11)]. In CHECKMATE-142, 74 patients with mCRC received OPDIVO 3 mg/kg by intravenous infusion over 60 minutes every 2 weeks until disease progression or until intolerable toxicity and 119 patients with mCRC received OPDIVO 3 mg/kg and ipilimumab 1 mg/kg every 3 weeks for 4 doses, then OPDIVO 3 mg/kg every 2 weeks until disease progression or until unacceptable toxicity.

In the OPDIVO with ipilimumab cohort, serious adverse reactions occurred in 47% of patients. Treatment was discontinued in 13% of patients and delayed in 45% of patients for an adverse reaction. The most frequent serious adverse reactions reported in ≥2% of patients were colitis/diarrhea, hepatic events, abdominal pain, acute kidney injury, pyrexia, and dehydration. The most common adverse reactions (reported in ≥20% of patients) were fatigue, diarrhea, pyrexia, musculoskeletal pain, abdominal pain, pruritus, nausea, rash, decreased appetite, and vomiting.

Tables 41 and 42 summarize adverse reactions and laboratory abnormalities, respectively, in CHECKMATE-142. Based on the design of CHECKMATE-142, the data below cannot be used to identify statistically significant differences between the two cohorts summarized below for any adverse reaction.

Table 41: Adverse Reactions Occurring in ≥10% of Patients - CHECKMATE-142
Adverse Reaction | OPDIVO (n=74) |  | OPDIVO and Ipilimumab (n=119)
Adverse Reaction | All Grades (%) | Grades 3-4 (%) | All Grades (%) | Grades 3-4 (%)
General
Fatiguea | 54 | 5 | 49 | 6
Pyrexia | 24 | 0 | 36 | 0
Edemab | 12 | 0 | 7 | 0
Gastrointestinal
Diarrhea | 43 | 2.7 | 45 | 3.4
Abdominal painc | 34 | 2.7 | 30 | 5
Nausea | 34 | 1.4 | 26 | 0.8
Vomiting | 28 | 4.1 | 20 | 1.7
Constipation | 20 | 0 | 15 | 0
Musculoskeletal and Connective Tissue
Musculoskeletal paind | 28 | 1.4 | 36 | 3.4
Arthralgia | 19 | 0 | 14 | 0.8
Respiratory, Thoracic and Mediastinal
Cough | 26 | 0 | 19 | 0.8
Dyspnea | 8 | 1 | 13 | 1.7
Skin and Subcutaneous Tissue
Rashe | 23 | 1.4 | 25 | 4.2
Pruritus | 19 | 0 | 28 | 1.7
Dry Skin | 7 | 0 | 11 | 0
Infections
Upper respiratory tract infectionf | 20 | 0 | 9 | 0
Endocrine
Hyperglycemia | 19 | 2.7 | 6 | 1
Hypothyroidism | 5 | 0 | 14 | 0.8
Hyperthyroidism | 4 | 0 | 12 | 0
Nervous System
Headache | 16 | 0 | 17 | 1.7
Dizziness | 14 | 0 | 11 | 0
Metabolism and Nutrition
Decreased appetite | 14 | 1.4 | 20 | 1.7
Psychiatric
Insomnia | 9 | 0 | 13 | 0.8
Investigations
Weight decreased | 8 | 0 | 10 | 0
Toxicity was graded per NCI CTCAE v4.
a Includes asthenia.
b Includes peripheral edema and peripheral swelling.
c Includes upper abdominal pain, lower abdominal pain, and abdominal discomfort.
d Includes back pain, pain in extremity, myalgia, neck pain, and bone pain.
e Includes dermatitis, dermatitis acneiform, and rash described as maculo-papular, erythematous, and generalized.
f Includes nasopharyngitis and rhinitis.

Clinically important adverse reactions reported in <10% of patients receiving OPDIVO with ipilimumab were encephalitis (0.8%), necrotizing myositis (0.8%), and uveitis (0.8%).

Table 42: Laboratory Abnormalities Worsening from Baselinea Occurring in ≥10% of Patients - CHECKMATE-142
Laboratory Abnormality | OPDIVO (n=74) |  | OPDIVO and Ipilimumab (n=119)
Laboratory Abnormality | All Grades (%) | Grades 3-4 (%) | All Grades (%) | Grades 3-4 (%)
Hematology
Anemia | 50 | 7 | 42 | 9
Lymphopenia | 36 | 7 | 25 | 6
Neutropenia | 20 | 4.3 | 18 | 0
Thrombocytopenia | 16 | 1.4 | 26 | 0.9
Chemistry
Increased alkaline phosphatase | 37 | 2.8 | 28 | 5
Increased lipase | 33 | 19 | 39 | 12
Increased ALT | 32 | 2.8 | 33 | 12
Increased AST | 31 | 1.4 | 40 | 12
Hyponatremia | 27 | 4.3 | 26 | 5
Hypocalcemia | 19 | 0 | 16 | 0
Hypomagnesemia | 17 | 0 | 18 | 0
Increased amylase | 16 | 4.8 | 36 | 3.4
Increased bilirubin | 14 | 4.2 | 21 | 5
Hypokalemia | 14 | 0 | 15 | 1.8
Increased creatinine | 12 | 0 | 25 | 3.6
Hyperkalemia | 11 | 0 | 23 | 0.9
a Each test incidence is based on the number of patients who had both baseline and at least one on-study laboratory measurement available. Number of evaluable patients ranges from 62 to 71 for the OPDIVO cohort and from 87 to 114 for the OPDIVO and ipilimumab cohort.

Hepatocellular Carcinoma

Unresectable or Metastatic Hepatocellular Carcinoma (HCC)

The safety of OPDIVO in combination with ipilimumab was evaluated in CHECKMATE-9DW, a randomized, open-label trial in adult patients with unresectable or metastatic HCC [see Clinical Studies (14.12)]. Patients received OPDIVO in combination with ipilimumab (n=332) or investigator’s choice of lenvatinib (n=275) or sorafenib (n=50) at the following dosage:

- OPDIVO 1 mg/kg administered intravenously over 30 minutes in combination with ipilimumab 3 mg/kg administered intravenously over 30 minutes every 3 weeks, for a maximum of 4 doses, followed by single-agent OPDIVO at 480 mg administered intravenously over 30 minutes every 4 weeks, or
- Investigator’s choice:
  - Lenvatinib 8 mg orally daily (if body weight <60 kg) or 12 mg orally daily (if body weight ≥60 kg), or
  - Sorafenib 400 mg orally twice daily

In the OPDIVO and ipilimumab arm, the median duration of exposure to OPDIVO was 4.7 months (range: <0.1 to 24.4 months), 45% were exposed for >6 months and 30% were exposed for >1 year.

Serious adverse reactions occurred in 53% of patients treated with OPDIVO in combination with ipilimumab. The most frequent non-liver-related serious adverse reactions reported in ≥2% of patients who received OPDIVO in combination with ipilimumab were diarrhea/colitis (4.5%), gastrointestinal hemorrhage (3%), and rash (2.4%).

Liver-related serious adverse reactions occurred in 17% of patients treated with OPDIVO in combination with ipilimumab, including Grade 3-4 events in 16% of patients. The most frequently reported all grade liver-related serious adverse reactions occurring in ≥1% of patients who received OPDIVO in combination with ipilimumab were immune-mediated hepatitis (3%), increased AST/ALT (3%), hepatic failure (2.4%), ascites (2.4%), and hepatotoxicity (1.2%).

Fatal adverse reactions occurred in 12 (3.6%) patients who received OPDIVO in combination with ipilimumab; these included 4 (1.2%) patients who died due to immune-mediated or autoimmune hepatitis and 4 (1.2%) patients who died of hepatic failure.

Permanent discontinuations of OPDIVO due to an adverse reaction occurred in 27% of patients. Adverse reactions leading to permanent discontinuation of OPDIVO in >1% of patients included immune-mediated hepatitis (1.8%), diarrhea/colitis (1.8%), hepatic failure (1.2%).

Dosage interruptions of OPDIVO due to an adverse reaction occurred in 62% of patients. Adverse reactions which required dosage interruption in >5% of patients included increased AST (13%), increased ALT (11%), and diarrhea/colitis (8%).

The most common (>20%) adverse reactions were rash, pruritus, fatigue, and diarrhea.

Tables 43 and 44 summarize the adverse reactions and laboratory abnormalities, respectively, in CHECKMATE-9DW.

Table 43: Adverse Reactions Occurring in ≥10% of OPDIVO in combination with Ipilimumab-Treated Patients - CHECKMATE-9DW
Adverse Reaction | OPDIVO and Ipilimumab; (n=332) |  | Lenvatinib or Sorafenib; (n=325)
Adverse Reaction | All Grades (%) | Grades 3-4 (%) | All Grades (%) | Grades 3-4 (%)
Skin and Subcutaneous Tissue
Rasha | 36 | 3.6 | 15 | 1.2
Pruritus | 34 | 1.5 | 7 | 0.3
General
Fatiguea | 33 | 2.4 | 39 | 4
Pyrexiaa | 15 | 0.6 | 9 | 1.5
Edemaa | 13 | 1.2 | 13 | 1.5
Gastrointestinal
Diarrheaa | 25 | 6 | 39 | 3.4
Abdominal paina | 14 | 1.2 | 27 | 2.5
Nausea | 10 | 0.3 | 16 | 0.9
Musculoskeletal and Connective Tissue
Musculoskeletal paina | 17 | 0.6 | 23 | 0.3
Arthralgia | 12 | 0.3 | 13 | 0.6
Metabolism and Nutrition
Decreased appetite | 16 | 1.2 | 28 | 1.8
Endocrine
Hypothyroidisma | 14 | 0 | 27 | 0
Hyperthyroidism | 11 | 0.6 | 1.5 | 0
Respiratory, Thoracic and Mediastinal
Cougha | 13 | 0 | 8 | 0
Toxicity was graded per NCI CTCAE v5
a Represents a composite of multiple related terms.

Clinically important adverse reactions reported in <10% of patients who received OPDIVO with ipilimumab were hyperglycemia (8%), adrenal insufficiency (4.2%), pneumonitis (2.7%), and pancreatitis (2.4%).

Table 44: Laboratory Values Worsening from Baselinea Occurring in ≥20% of OPDIVO in combination with Ipilimumab-Treated Patients - CHECKMATE-9DW
Laboratory Abnormality | OPDIVO and Ipilimumab; (n=332) |  | Lenvatinib or Sorafenib; (n=325)
Laboratory Abnormality | Grades 1-4 (%) | Grades 3-4 (%) | Grades 1-4 (%) | Grades 3-4 (%)
Chemistry
Increased AST | 62 | 29 | 51 | 14
Increased ALT | 61 | 17 | 46 | 9
Increased lipase | 58 | 16 | 39 | 5
Decreased albumin | 48 | 0.9 | 57 | 0.6
Hyponatremia | 45 | 6 | 42 | 3.8
Hyperglycemia | 44 | 15 | 32 | 2.1
Increased bilirubin | 44 | 10 | 44 | 8
Increased amylase | 41 | 6 | 26 | 1
Increased alkaline phosphatase | 36 | 1.2 | 38 | 5
Hypocalcemia | 29 | 0.9 | 46 | 0
Increased creatinine | 26 | 2.4 | 23 | 0.6
Hypokalemia | 21 | 2.1 | 20 | 2.6
Hematology
Anemia | 44 | 5 | 40 | 3.8
Lymphopenia | 40 | 6.1 | 40 | 8
Thrombocytopenia | 27 | 4 | 44 | 4.8
Neutropenia | 24 | 4 | 32 | 3.5
a Each test incidence is based on the number of patients who had both baseline and at least one on-study laboratory measurement available: OPDIVO and ipilimumab group (range: 168 to 331 patients) and lenvatinib or sorafenib group (range: 145 to 315 patients).

Previously Treated Hepatocellular Carcinoma

The safety of OPDIVO 1 mg/kg in combination with ipilimumab 3 mg/kg was evaluated in a subgroup comprising 49 patients with HCC and Child-Pugh Class A cirrhosis enrolled in Cohort 4 of CHECKMATE-040, a multicenter, multiple-cohort, open-label trial [see Clinical Studies (14.12)] who progressed on or were intolerant to sorafenib. OPDIVO and ipilimumab were administered every 3 weeks for 4 doses, followed by single-agent OPDIVO 240 mg every 2 weeks until disease progression or unacceptable toxicity. During the OPDIVO and ipilimumab combination period, 33 of 49 (67%) patients received all 4 planned doses of OPDIVO and ipilimumab. During the entire treatment period, the median duration of exposure to OPDIVO was 5.1 months (range: 0 to 35+ months) and to ipilimumab was 2.1 months (range: 0 to 4.5 months). Forty-seven percent of patients were exposed to treatment for >6 months, and 35% of patients were exposed to treatment for >1 year. Serious adverse reactions occurred in 59% of patients. Treatment was discontinued in 29% of patients and delayed in 65% of patients for an adverse reaction.

The most frequent serious adverse reactions (reported in ≥4% of patients) were pyrexia, diarrhea, anemia, increased AST, adrenal insufficiency, ascites, esophageal varices hemorrhage, hyponatremia, increased blood bilirubin, and pneumonitis.

Tables 45 and 46 summarize the adverse reactions and laboratory abnormalities, respectively, in CHECKMATE-040.

Table 45: Adverse Reactions Occurring in ≥10% of Patients Receiving OPDIVO in Combination with Ipilimumab in Cohort 4 of CHECKMATE-040
Adverse Reaction | OPDIVO and Ipilimumab; (n=49)
Adverse Reaction | All Grades (%) | Grades 3-4 (%)
Skin and Subcutaneous Tissue
Rash | 53 | 8
Pruritus | 53 | 4
Musculoskeletal and Connective Tissue
Musculoskeletal pain | 41 | 2
Arthralgia | 10 | 0
Gastrointestinal
Diarrhea | 39 | 4
Abdominal pain | 22 | 6
Nausea | 20 | 0
Ascites | 14 | 6
Constipation | 14 | 0
Dry mouth | 12 | 0
Dyspepsia | 12 | 2
Vomiting | 12 | 2
Stomatitis | 10 | 0
Respiratory, Thoracic and Mediastinal
Cough | 37 | 0
Dyspnea | 14 | 0
Pneumonitis | 10 | 2
Metabolism and Nutrition
Decreased appetite | 35 | 2
General
Fatigue | 27 | 2
Pyrexia | 27 | 0
Malaise | 18 | 2
Edema | 16 | 2
Influenza-like illness | 14 | 0
Chills | 10 | 0
Nervous System
Headache | 22 | 0
Dizziness | 20 | 0
Endocrine
Hypothyroidism | 20 | 0
Adrenal insufficiency | 18 | 4
Investigations
Weight decreased | 20 | 0
Psychiatric
Insomnia | 18 | 0
Blood and Lymphatic System
Anemia | 10 | 4
Infections
Influenza | 10 | 2
Vascular
Hypotension | 10 | 0

Clinically important adverse reactions reported in <10% of patients who received OPDIVO with ipilimumab were hyperglycemia (8%), colitis (4%), and increased blood creatine phosphokinase (2%).

Table 46: Laboratory Abnormalities Worsening from Baseline Occurring in ≥10% of Patients Receiving OPDIVO in Combination with Ipilimumab in Cohort 4 of CHECKMATE-040
Laboratory Abnormality | OPDIVO and Ipilimumab; (n=47)
Laboratory Abnormality | All Grades (%) | Grades 3-4 (%)
Hematology
Lymphopenia | 53 | 13
Anemia | 43 | 4.3
Neutropenia | 43 | 9
Leukopenia | 40 | 2.1
Thrombocytopenia | 34 | 4.3
Chemistry
Increased AST | 66 | 40
Increased ALT | 66 | 21
Increased bilirubin | 55 | 11
Increased lipase | 51 | 26
Hyponatremia | 49 | 32
Hypocalcemia | 47 | 0
Increased alkaline phosphatase | 40 | 4.3
Increased amylase | 38 | 15
Hypokalemia | 26 | 2.1
Hyperkalemia | 23 | 4.3
Increased creatinine | 21 | 0
Hypomagnesemia | 11 | 0

In patients who received OPDIVO with ipilimumab, virologic breakthrough occurred in 4 of 28 (14%) patients and 2 of 4 (50%) patients with active HBV or HCV at baseline, respectively. HBV virologic breakthrough was defined as at least a 1 log increase in HBV DNA for those patients with detectable HBV DNA at baseline. HCV virologic breakthrough was defined as a 1 log increase in HCV RNA from baseline.

Esophageal Cancer

Adjuvant Treatment of Resected Esophageal or Gastroesophageal Junction Cancer

The safety of OPDIVO was evaluated in CHECKMATE-577, a randomized, placebo-controlled, double-blinded, multicenter trial in 792 treated patients with completely resected (negative margins) esophageal or gastroesophageal junction cancer who had residual pathologic disease following chemoradiotherapy (CRT) [see Clinical Studies (14.13)]. The trial excluded patients who did not receive concurrent CRT prior to surgery, had stage IV resectable disease, autoimmune disease, or any condition requiring systemic treatment with either corticosteroids (>10 mg daily prednisone or equivalent) or other immunosuppressive medications. Patients received either OPDIVO 240 mg or placebo by intravenous infusion over 30 minutes every 2 weeks for 16 weeks followed by 480 mg or placebo by intravenous infusion over 30 minutes every 4 weeks beginning at week 17. Patients were treated until disease recurrence, unacceptable toxicity, or for up to 1-year total duration. The median duration of exposure was 10.1 months (range: <0.1 to 14 months) in OPDIVO-treated patients and 9 months (range: <0.1 to 15 months) in placebo-treated patients. Among patients who received OPDIVO, 61% were exposed for >6 months and 54% were exposed for >9 months.

Serious adverse reactions occurred in 33% of patients receiving OPDIVO. A serious adverse reaction reported in ≥2% of patients who received OPDIVO was pneumonitis. A fatal adverse reaction of myocardial infarction occurred in one patient who received OPDIVO.

OPDIVO was discontinued in 12% of patients and was delayed in 28% of patients for an adverse reaction.

Tables 47 and 48 summarize the adverse reactions and laboratory abnormalities, respectively, in CHECKMATE-577.

Table 47: Adverse Reactions Occurring in ≥10% of Patients Receiving OPDIVO - CHECKMATE-577
Adverse Reaction | OPDIVO; (n=532) |  | Placebo; (n=260)
Adverse Reaction | All Grades (%) | Grades 3-4 (%) | All Grades (%) | Grades 3-4 (%)
Adverse Reaction | 96 | 34 | 93 | 32
Gastrointestinal
Diarrhea | 29 | 0.9 | 29 | 0.8
Nausea | 23 | 0.8 | 21 | 0
Abdominal Paina | 17 | 0.8 | 20 | 1.5
Vomiting | 15 | 0.6 | 16 | 1.2
Dysphagia | 13 | 0.8 | 17 | 3.5
Dyspepsiab | 12 | 0.2 | 16 | 0.4
Constipation | 11 | 0 | 12 | 0
General
Fatiguec | 34 | 1.3 | 29 | 1.5
Respiratory, Thoracic and Mediastinal
Coughd | 20 | 0.2 | 21 | 0.4
Dyspneae | 12 | 0.8 | 12 | 0.4
Skin and Subcutaneous Tissue
Rashf | 21 | 0.9 | 10 | 0.4
Pruritus | 13 | 0.4 | 6 | 0
Investigations
Weight decreased | 13 | 0.4 | 9 | 0
Musculoskeletal and Connective Tissue
Musculoskeletal paing | 21 | 0.6 | 20 | 0.8
Arthralgia | 10 | 0.2 | 8 | 0
Metabolism and Nutrition
Decreased appetite | 15 | 0.9 | 10 | 0.8
Endocrine
Hypothyroidism | 11 | 0 | 1.5 | 0
a Includes upper abdominal pain, lower abdominal pain, and abdominal discomfort.
b Includes gastroesophageal reflux.
c Includes asthenia.
d Includes productive cough.
e Includes dyspnea exertional.
f Includes rash pustular, dermatitis, dermatitis acneiform, dermatitis allergic, dermatitis bullous, exfoliative rash, rash erythematous, rash macular, rash maculo-papular, rash papular, rash pruritic.
g Includes back pain, bone pain, musculoskeletal chest pain, musculoskeletal discomfort, myalgia, myalgia intercostal, neck pain, pain in extremity, spinal pain.

Table 48: Laboratory Abnormalities Worsening from Baselinea Occurring in ≥10% of Patients - CHECKMATE-577
Laboratory Abnormality | OPDIVO; (n=532) |  | Placebo; (n=260)
Laboratory Abnormality | All Grades (%) | Grades 3-4 (%) | All Grades (%) | Grades 3-4 (%)
Chemistry
Increased AST | 27 | 2.1 | 22 | 0.8
Increased alkaline phosphatase | 25 | 0.8 | 18 | 0.8
Increased albumin | 21 | 0.2 | 18 | 0
Increased ALT | 20 | 1.9 | 16 | 1.2
Increased amylase | 20 | 3.9 | 13 | 1.3
Hyponatremia | 19 | 1.7 | 12 | 1.2
Hyperkalemia | 17 | 0.8 | 15 | 1.6
Hypokalemia | 12 | 1 | 11 | 1.2
Transaminases increasedb | 11 | 1.5 | 6 | 1.2
Hematology
Lymphopenia | 44 | 17 | 35 | 12
Anemia | 27 | 0.8 | 21 | 0.4
Neutropenia | 24 | 1.5 | 23 | 0.4
a Each test incidence is based on the number of patients who had both baseline and at least one on-study laboratory measurement available: OPDIVO group (range: 163 to 526 patients) and Placebo group (range: 86 to 256 patients).
b Includes alanine aminotransferase increased, aspartate aminotransferase increased.

First-line Treatment of Unresectable Advanced or Metastatic ESCC

The safety of OPDIVO in combination with chemotherapy or in combination with ipilimumab was evaluated in CHECKMATE-648, a randomized, active-controlled, multicenter, open-label trial in patients with previously untreated unresectable advanced, recurrent or metastatic ESCC [see Clinical Studies (14.13)]. Patients received one of the following treatments:

- OPDIVO 240 mg on days 1 and 15, 5-FU (fluorouracil) 800 mg/m^2/day intravenously on days 1 through 5 (for 5 days), and cisplatin 80 mg/m^2 intravenously on day 1 (of a 4-week cycle).
- OPDIVO 3 mg/kg every 2 weeks in combination with ipilimumab 1 mg/kg every 6 weeks.
- 5-FU (fluorouracil) 800 mg/m^2/day intravenously on days 1 through 5 (for 5 days), and cisplatin 80 mg/m^2 intravenously on day 1 (of a 4-week cycle).

Among patients who received OPDIVO with chemotherapy, the median duration of exposure was 5.7 months (range: 0.1 to 30.6 months). Among patients who received OPDIVO and ipilimumab, the median duration of exposure was 2.8 months (range: 0 to 24 months).

Serious adverse reactions occurred in 62% of patients receiving OPDIVO in combination with chemotherapy and in 69% of patients receiving OPDIVO in combination with ipilimumab. The most frequent serious adverse reactions reported in ≥2% of patients who received OPDIVO with chemotherapy were pneumonia (11%), dysphagia (7%), esophageal stenosis (2.9%), acute kidney injury (2.9%), and pyrexia (2.3%). The most frequent serious adverse reactions reported in ≥2% of patients who received OPDIVO with ipilimumab were pneumonia (10%), pyrexia (4.3%), pneumonitis (4%), aspiration pneumonia (3.7%), dysphagia (3.7%), hepatic function abnormal (2.8%), decreased appetite (2.8%), adrenal insufficiency (2.5%), and dehydration (2.5%).

Fatal adverse reactions occurred in 5 (1.6%) patients who received OPDIVO in combination with chemotherapy; these included pneumonitis, pneumatosis intestinalis, pneumonia, and acute kidney injury and in 5 (1.6%) patients who received OPDIVO in combination with ipilimumab; these included pneumonitis, interstitial lung disease, pulmonary embolism, and acute respiratory distress syndrome.

OPDIVO and/or chemotherapy were discontinued in 39% of patients and were delayed in 71% of patients for an adverse reaction. OPDIVO and/or ipilimumab were discontinued in 23% of patients and were delayed in 46% of patients for an adverse reaction.

The most common adverse reactions reported in ≥20% of patients treated with OPDIVO in combination with chemotherapy were nausea, decreased appetite, fatigue, constipation, stomatitis, diarrhea, and vomiting. The most common adverse reactions reported in ≥20% of patients treated with OPDIVO in combination with ipilimumab were rash, fatigue, pyrexia, nausea, diarrhea, and constipation.

Tables 49 and 50 summarize the adverse reactions and laboratory abnormalities, respectively, in CHECKMATE-648.

Table 49: Adverse Reactions in ≥10% of Patients - CHECKMATE-648
Adverse Reaction | OPDIVO with Cisplatin and 5‑FU; (n=310) |  | OPDIVO and Ipilimumab; (n=322) |  | Cisplatin and 5-FU (n=304)
Adverse Reaction | All Grades (%) | Grades 3-4 (%) | All Grades (%) | Grades 3-4 (%) | All Grades (%) | Grades 3-4 (%)
Gastrointestinal
Nausea | 65 | 4.2 | 22 | 0.6 | 56 | 2.6
Constipation | 44 | 1.0 | 20 | 0.3 | 43 | 1
Stomatitisa | 44 | 9 | 11 | 0.6 | 35 | 3
Diarrhea | 29 | 2.9 | 22 | 1.9 | 20 | 2
Vomiting | 23 | 2.3 | 15 | 1.6 | 19 | 3
Dysphagia | 14 | 7 | 12 | 5 | 12 | 4.9
Abdominal painb | 13 | 1.9 | 10 | 0.9 | 11 | 0.7
Metabolism and Nutrition
Decreased appetite | 51 | 7 | 17 | 4 | 50 | 6
General
Fatiguec | 47 | 3.5 | 28 | 2.5 | 41 | 4.9
Pyrexiad | 19 | 0.3 | 23 | 0.9 | 12 | 0.3
Edemae | 16 | 0 | 7 | 0 | 13 | 0
Nervous System
Peripheral neuropathyf | 18 | 1.3 | 2.8 | 0 | 13 | 1
Psychiatric
Insomnia | 16 | 0 | 8 | 0 | 10 | 0.3
Skin and Subcutaneous Tissue
Rashg | 16 | 0.6 | 31 | 3.1 | 7 | 0
Pruritus | 11 | 0 | 17 | 0.9 | 3.6 | 0
Alopecia | 10 | 0 |  |  | 11 | 0
Respiratory, Thoracic and Mediastinal
Coughh | 16 | 0.3 | 13 | 0.3 | 13 | 0.3
Infections and Infestations
Pneumoniai | 13 | 5 | 14 | 8 | 10 | 2.6
Endocrine
Hypothyroidism | 7 | 0 | 14 | 0 | 0.3 | 0
Investigations
Weight decreased | 12 | 0.6 | 12 | 1.9 | 11 | 1
Musculoskeletal and Connective Tissue
Musculoskeletal painj | 11 | 0.3 | 14 | 0.6 | 8 | 0.3
Toxicity was graded per NCI CTCAE v4.
a Includes aphthous ulcer, mouth ulceration, and mucosal inflammation.
b Includes abdominal discomfort, abdominal pain lower, and abdominal pain upper.
c Includes asthenia and malaise.
d Includes tumor associated fever.
e Includes swelling, generalized edema, edema peripheral, and peripheral swelling.
f Includes hyperesthesia, hypoesthesia, peripheral motor neuropathy, peripheral sensorimotor neuropathy, and peripheral sensory neuropathy.
g Includes dermatitis, dermatitis acneiform, dermatitis allergic, dermatitis bullous, drug eruption, exfoliative rash, rash erythematous, rash follicular, rash macular, rash maculo-papular, rash papular, and rash pruritic.
h Includes productive cough.
i Includes organizing pneumonia, pneumonia bacterial, and pneumonia pseudomonal.
j Includes back pain, bone pain, musculoskeletal chest pain, myalgia, neck pain, pain in extremity, and spinal pain.

Table 50: Laboratory Values Worsening from Baselinea Occurring in ≥10% of Patients - CHECKMATE-648
Laboratory Abnormality | OPDIVO with Cisplatin and 5-FU (n=310) |  | OPDIVO and Ipilimumab (n=322) |  | Cisplatin and 5-FU (n=304)
Laboratory Abnormality | Grades 1-4 (%) | Grades 3-4 (%) | Grades 1-4 (%) | Grades 3-4 (%) | Grades 1-4 (%) | Grades 3-4 (%)
Hematology
Anemia | 81 | 21 | 52 | 7 | 66 | 14
Lymphopenia | 67 | 23 | 50 | 13 | 44 | 8
Neutropenia | 61 | 18 | 13 | 1.3 | 48 | 13
Leukopenia | 53 | 11 |  |  | 39 | 5
Thrombocytopenia | 43 | 3.3 | 12 | 1 | 29 | 2.8
Chemistry
Hyponatremia | 52 | 15 | 45 | 11 | 40 | 8
Hypocalcemia | 43 | 3 | 32 | 0 | 23 | 0.7
Increased creatinine | 41 | 2.3 | 15 | 0.7 | 31 | 0.7
Hypomagnesemia | 35 | 1.7 | 15 | 0 | 25 | 1.8
Hyperglycemia | 34 | 0 | 43 | 4.3 | 36 | 0.8
Hyperkalemia | 33 | 2.3 | 23 | 1.6 | 24 | 0.7
Hypokalemia | 29 | 9 | 19 | 5 | 17 | 6
Increased alkaline; phosphatase | 26 | 1.3 | 31 | 3.3 | 15 | 0
Increased AST | 23 | 3.3 | 39 | 6 | 11 | 1.4
Increased ALT | 23 | 2.3 | 33 | 6 | 8 | 0.7
Hypoglycemia | 18 | 0.4 | 15 | 1.2 | 7 | 0
Hypercalcemia | 11 | 2.6 | 15 | 2 | 8 | 0
a Each test incidence is based on the number of patients who had both baseline and at least one on-study laboratory measurement available: OPDIVO with cisplatin and 5-FU group (range: 60 to 305 patients), OPDIVO and ipilimumab group (range: 59 to 307 patients) or cisplatin and 5-FU group (range: 56 to 283 patients).

Previously-Treated Unresectable Advanced, Recurrent or Metastatic Esophageal Squamous Cell Carcinoma (ESCC)

The safety of OPDIVO was evaluated in ATTRACTION-3, a randomized, active-controlled, open-label, multicenter trial in 209 patients with unresectable advanced, recurrent or metastatic ESCC refractory or intolerant to at least one fluoropyrimidine- and platinum-based chemotherapy [see Clinical Studies (14.13)]. The trial excluded patients who were refractory or intolerant to taxane therapy, had brain metastases that were symptomatic or required treatment, had autoimmune disease, used systemic corticosteroids or immunosuppressants, had apparent tumor invasion of organs adjacent to the esophageal tumor or had stents in the esophagus or respiratory tract. Patients received OPDIVO 240 mg by intravenous infusion over 30 minutes every 2 weeks (n=209) or investigator’s choice: docetaxel 75 mg/m^2 intravenously every 3 weeks (n=65) or paclitaxel 100 mg/m^2 intravenously once a week for 6 weeks followed by 1 week off (n=143). Patients were treated until disease progression or unacceptable toxicity. The median duration of exposure was 2.6 months (range: 0 to 29.2 months) in OPDIVO-treated patients and 2.6 months (range: 0 to 21.4 months) in docetaxel- or paclitaxel-treated patients. Among patients who received OPDIVO, 26% were exposed for >6 months and 10% were exposed for >1 year.

Serious adverse reactions occurred in 38% of patients receiving OPDIVO. Serious adverse reactions reported in ≥2% of patients who received OPDIVO were pneumonia, esophageal fistula, interstitial lung disease and pyrexia. The following fatal adverse reactions occurred in patients who received OPDIVO: interstitial lung disease or pneumonitis (1.4%), pneumonia (1.0%), septic shock (0.5%), esophageal fistula (0.5%), gastrointestinal hemorrhage (0.5%), pulmonary embolism (0.5%), and sudden death (0.5%).

OPDIVO was discontinued in 13% of patients and was delayed in 27% of patients for an adverse reaction.

Tables 51 and 52 summarize the adverse reactions and laboratory abnormalities, respectively, in ATTRACTION-3.

Table 51: Adverse Reactions Occurring in ≥10% of Patients Receiving OPDIVO - ATTRACTION-3
Adverse Reaction | OPDIVO; (n=209) |  | Docetaxel or Paclitaxel; (n=208)
Adverse Reaction | All Grades (%) | Grades 3-4 (%) | All Grades (%) | Grades 3-4 (%)
Skin and Subcutaneous Tissue
Rasha | 22 | 1.9 | 28 | 1
Pruritus | 12 | 0 | 7 | 0
Metabolism and Nutrition
Decreased appetiteb | 21 | 1.9 | 35 | 5
Gastrointestinal
Diarrheac | 18 | 1.9 | 17 | 1.4
Constipation | 17 | 0 | 19 | 0
Nausea | 11 | 0 | 20 | 0.5
Musculoskeletal and Connective Tissue
Musculoskeletal paind | 17 | 0 | 26 | 1.4
Infections
Upper respiratory tract infectione | 17 | 1 | 14 | 0
Pneumoniaf | 13 | 5 | 19 | 9
Respiratory, Thoracic and Mediastinal
Coughg | 16 | 0 | 14 | 0.5
General
Pyrexiah | 16 | 0.5 | 19 | 0.5
Fatiguei | 12 | 1.4 | 27 | 4.8
Blood and Lymphatic System
Anemiaj | 13 | 8 | 30 | 13
Endocrine
Hypothyroidismk | 11 | 0 | 1.4 | 0
Toxicity was graded per NCI CTCAE v4.
a Includes urticaria, drug eruption, eczema, eczema asteatotic, eczema nummular, palmar-plantar erythrodysesthesia syndrome, erythema, erythema multiforme, blister, skin exfoliation, Stevens-Johnson syndrome, dermatitis, dermatitis described as acneiform, bullous, or contact, and rash described as maculo-papular, generalized, or pustular.
b Includes hypophagia, and food aversion.
c Includes colitis.
d Includes spondylolisthesis, periarthritis, musculoskeletal chest pain, neck pain, arthralgia, back pain, myalgia, pain in extremity, arthritis, bone pain, and periarthritis calcarea.
e Includes influenza, influenza like illness, pharyngitis, nasopharyngitis, tracheitis, and bronchitis and upper respiratory infection with bronchitis.
f Includes pneumonia aspiration, pneumonia bacterial, and lung infection. Two patients (1.0%) died of pneumonia in the OPDIVO treatment arm. Two patients (1.0%) died of pneumonia in the chemotherapy treatment arm; these deaths occurred with paclitaxel only.
g Includes productive cough.
h Includes tumor-associated fever.
i Includes asthenia.
j Includes hemoglobin decreased, and iron deficiency anemia.
k Includes blood thyroid stimulating hormone increased.

Table 52: Laboratory Abnormalities Worsening from Baselinea Occurring in ≥10% of Patients - ATTRACTION-3
Laboratory Abnormality | OPDIVO; (n=209) |  | Docetaxel or Paclitaxel; (n=208)
Laboratory Abnormality | All Grades (%) | Grades 3-4 (%) | All Grades (%) | Grades 3-4 (%)
Chemistry
Increased creatinine | 78 | 0.5 | 68 | 0.5
Hyperglycemia | 52 | 5 | 62 | 5
Hyponatremia | 42 | 11 | 50 | 12
Increased AST | 40 | 6 | 30 | 1
Increased alkaline phosphatase | 33 | 4.8 | 24 | 1.0
Increased ALT | 31 | 5 | 22 | 1.9
Hypercalcemia | 22 | 6 | 14 | 2.9
Hyperkalemia | 22 | 0.5 | 31 | 1
Hypoglycemia | 14 | 1.4 | 14 | 0.5
Hypokalemia | 11 | 2.9 | 13 | 3.4
Hematology
Lymphopenia | 46 | 19 | 72 | 43
Anemia | 42 | 9 | 71 | 17
Leukopenia | 11 | 0.5 | 79 | 45
a Each test incidence is based on the number of patients who had both baseline and at least one on-study laboratory measurement available: OPDIVO group (209 patients) and Docetaxel or Paclitaxel group (range: 207 to 208 patients).

Gastric Cancer, Gastroesophageal Junction Cancer, and Esophageal Adenocarcinoma

The safety of OPDIVO in combination with chemotherapy was evaluated in CHECKMATE-649, a randomized, multicenter, open-label trial in patients with previously untreated advanced or metastatic gastric cancer, gastroesophageal junction cancer, and esophageal adenocarcinoma [see Clinical Studies (14.14)]. The trial excluded patients who were known human epidermal growth factor receptor 2 (HER2) positive or had untreated central nervous system (CNS) metastases. Patients were randomized to receive OPDIVO in combination with chemotherapy or chemotherapy. Patients received one of the following treatments:

- OPDIVO 240 mg in combination with mFOLFOX6 (fluorouracil, leucovorin and oxaliplatin) every 2 weeks or mFOLFOX6 every 2 weeks.
- OPDIVO 360 mg in combination with CapeOX (capecitabine and oxaliplatin) every 3 weeks or CapeOX every 3 weeks.

Patients were treated with OPDIVO in combination with chemotherapy or chemotherapy until disease progression, unacceptable toxicity, or up to 2 years. The median duration of exposure was 6.8 months (range: 0 to 33.5 months) in OPDIVO and chemotherapy-treated patients. Among patients who received OPDIVO and chemotherapy, 54% were exposed for >6 months and 28% were exposed for >1 year.

Fatal adverse reactions occurred in 16 (2.0%) patients who were treated with OPDIVO in combination with chemotherapy; these included pneumonitis (4 patients), febrile neutropenia (2 patients), stroke (2 patients), gastrointestinal toxicity, intestinal mucositis, septic shock, pneumonia, infection, gastrointestinal bleeding, mesenteric vessel thrombosis, and disseminated intravascular coagulation. Serious adverse reactions occurred in 52% of patients treated with OPDIVO in combination with chemotherapy. OPDIVO and/or chemotherapy were discontinued in 44% of patients and at least one dose was withheld in 76% of patients due to an adverse reaction.

The most frequent serious adverse reactions reported in ≥2% of patients treated with OPDIVO in combination with chemotherapy were vomiting (3.7%), pneumonia (3.6%), anemia (3.6%), pyrexia (2.8%), diarrhea (2.7%), febrile neutropenia (2.6%), and pneumonitis (2.4%). The most common adverse reactions reported in ≥20% of patients treated with OPDIVO in combination with chemotherapy were peripheral neuropathy, nausea, fatigue, diarrhea, vomiting, decreased appetite, abdominal pain, constipation, and musculoskeletal pain.

Tables 53 and 54 summarize the adverse reactions and laboratory abnormalities, respectively, in CHECKMATE-649.

Table 53: Adverse Reactions in ≥10% of Patients Receiving OPDIVO and Chemotherapy - CHECKMATE-649
Adverse Reaction | OPDIVO and mFOLFOX6 or CapeOX; (n=782) |  | mFOLFOX6 or CapeOX; (n=767)
Adverse Reaction | All Grades (%) | Grades 3-4 (%) | All Grades (%) | Grades 3-4 (%)
Adverse Reaction | 99 | 69 | 98 | 59
Nervous System
Peripheral neuropathya | 53 | 7 | 46 | 4.8
Headache | 11 | 0.8 | 6 | 0.3
Gastrointestinal
Nausea | 48 | 3.2 | 44 | 3.7
Diarrhea | 39 | 5 | 34 | 3.7
Vomiting | 31 | 4.2 | 29 | 4.2
Abdominal painb | 27 | 2.8 | 24 | 2.6
Constipation | 25 | 0.6 | 21 | 0.4
Stomatitisc | 17 | 1.8 | 13 | 0.8
General
Fatigued | 44 | 7 | 40 | 5
Pyrexiae | 19 | 1 | 11 | 0.4
Edemaf | 12 | 0.5 | 8 | 0.1
Metabolism and Nutrition
Decreased appetite | 29 | 3.6 | 26 | 2.5
Hypoalbuminemiag | 14 | 0.3 | 9 | 0.3
Investigations
Weight decreased | 17 | 1.3 | 15 | 0.7
Increased lipase | 14 | 7 | 8 | 3.7
Increased amylase | 12 | 3.1 | 5 | 0.4
Musculoskeletal and Connective Tissue
Musculoskeletal painh | 20 | 1.3 | 14 | 2
Skin and Subcutaneous Tissue
Rashi | 18 | 1.7 | 4.4 | 0.1
Palmar-plantar erythrodysesthesia syndrome | 13 | 1.5 | 12 | 0.8
Respiratory, Thoracic and Mediastinal
Coughj | 13 | 0.1 | 9 | 0
Infections and Infestations
Upper respiratory tract infectionk | 10 | 0.1 | 7 | 0.1
Toxicity was graded per NCI CTCAE v4.
a Includes dysesthesia, hypoesthesia, peripheral motor neuropathy, peripheral sensorimotor neuropathy, and peripheral sensory neuropathy.
b Includes abdominal discomfort, abdominal pain lower, and abdominal pain upper.
c Includes aphthous ulcer, mouth ulceration, and mucosal inflammation.
d Includes asthenia.
e Includes tumor associated fever.
f Includes swelling, generalized edema, edema peripheral, and peripheral swelling.
g Includes blood albumin decreased.
h Includes back pain, bone pain, musculoskeletal chest pain, musculoskeletal discomfort, myalgia, neck pain, pain in extremity, and spinal pain.
i Includes dermatitis, dermatitis acneiform, dermatitis allergic, dermatitis bullous, drug eruption, exfoliative rash, nodular rash, rash erythematous, rash macular, rash maculo-papular, rash papular, rash pruritic, and rash vesicular.
j Includes productive cough.
k Includes nasopharyngitis, pharyngitis, and rhinitis.

Table 54: Laboratory Values Worsening from Baselinea Occurring in ≥10% of Patients - CHECKMATE-649
Laboratory Abnormality | OPDIVO and mFOLFOX6 or CapeOX (n=782) |  | mFOLFOX6 or CapeOX (n=767)
Laboratory Abnormality | Grades 1-4 (%) | Grades 3-4 (%) | Grades 1-4 (%) | Grades 3-4 (%)
Hematology
Neutropenia | 73 | 29 | 62 | 23
Leukopenia | 69 | 12 | 59 | 9
Thrombocytopenia | 68 | 7 | 63 | 4.4
Anemia | 59 | 14 | 60 | 10
Lymphopenia | 59 | 12 | 49 | 9
Chemistry
Increased AST | 52 | 4.6 | 47 | 1.9
Hypocalcemia | 42 | 1.6 | 37 | 1
Hyperglycemia | 41 | 3.9 | 38 | 2.7
Increased ALT | 37 | 3.4 | 30 | 1.9
Hyponatremia | 34 | 6 | 24 | 5
Hypokalemia | 27 | 7 | 24 | 4.8
Hyperbilirubinemia | 24 | 2.8 | 21 | 2
Increased creatinine | 15 | 1 | 9 | 0.5
Hyperkalemia | 14 | 1.4 | 11 | 0.7
Hypoglycemia | 12 | 0.7 | 9 | 0.2
Hypernatremia | 11 | 0.5 | 7.1 | 0
a Each test incidence is based on the number of patients who had both baseline and at least one on-study laboratory measurement available: OPDIVO and mFOLFOX6 or CapeOX group (407 to 767 patients) or mFOLFOX6 or CapeOX group (range: 405 to 735 patients).

6.2 Postmarketing Experience

The following adverse reactions have been identified during post-approval use of OPDIVO. Because these reactions are reported voluntarily from a population of uncertain size, it is not always possible to reliably estimate their frequency or establish a causal relationship to drug exposure.

Eye: Vogt-Koyanagi-Harada (VKH) syndrome

Complications of OPDIVO Treatment After Allogeneic HSCT: Treatment refractory, severe acute and chronic GVHD

Blood and lymphatic system disorders: Hemophagocytic lymphohistiocytosis (HLH) (including fatal cases), autoimmune hemolytic anemia (including fatal cases)

Metabolism and nutrition disorders: tumor lysis syndrome

8 USE IN SPECIFIC POPULATIONS

8.1 Pregnancy

Risk Summary

Based on data from animal studies and its mechanism of action [see Clinical Pharmacology (12.1)], OPDIVO can cause fetal harm when administered to a pregnant woman. In animal reproduction studies, administration of nivolumab to cynomolgus monkeys from the onset of organogenesis through delivery resulted in increased abortion and premature infant death (see Data). Human IgG4 is known to cross the placental barrier and nivolumab is an immunoglobulin G4 (IgG4); therefore, nivolumab has the potential to be transmitted from the mother to the developing fetus. The effects of OPDIVO are likely to be greater during the second and third trimesters of pregnancy. There are no available data on OPDIVO use in pregnant women to evaluate a drug-associated risk. Advise pregnant women of the potential risk to a fetus.

The background risk in the U.S. general population of major birth defects is 2% to 4% and of miscarriage is 15% to 20% of clinically recognized pregnancies.

Data

Animal Data

A central function of the PD-1/PD-L1 pathway is to preserve pregnancy by maintaining maternal immune tolerance to the fetus. Blockade of PD-L1 signaling has been shown in murine models of pregnancy to disrupt tolerance to the fetus and to increase fetal loss. The effects of nivolumab on prenatal and postnatal development were evaluated in monkeys that received nivolumab twice weekly from the onset of organogenesis through delivery, at exposure levels of between 9 and 42 times higher than those observed at the clinical dose of 3 mg/kg (based on AUC). Nivolumab administration resulted in a non-dose-related increase in spontaneous abortion and increased neonatal death. Based on its mechanism of action, fetal exposure to nivolumab may increase the risk of developing immune-mediated disorders or altering the normal immune response and immune-mediated disorders have been reported in PD-1 knockout mice. In surviving infants (18 of 32 compared to 11 of 16 vehicle-exposed infants) of cynomolgus monkeys treated with nivolumab, there were no apparent malformations and no effects on neurobehavioral, immunological, or clinical pathology parameters throughout the 6-month postnatal period.

8.2 Lactation

Risk Summary

There are no data on the presence of nivolumab in human milk, the effects on the breastfed child, or the effects on milk production. Because of the potential for serious adverse reactions in the breastfed child, advise women not to breastfeed during treatment and for 5 months after the last dose of OPDIVO.

8.3 Females and Males of Reproductive Potential

Pregnancy Testing

Verify the pregnancy status of females of reproductive potential prior to initiating OPDIVO [see Use in Specific Populations (8.1)].

Contraception

OPDIVO can cause fetal harm when administered to a pregnant woman [see Use in Specific Populations (8.1)]. Advise females of reproductive potential to use effective contraception during treatment with OPDIVO and for 5 months following the last dose.

8.4 Pediatric Use

The safety and effectiveness of OPDIVO have been established in pediatric patients aged 12 years and older for the following indications: as a single agent and in combination with ipilimumab for the treatment of unresectable or metastatic melanoma, as a single agent for the adjuvant treatment of completely resected Stage IIB, Stage IIC, Stage III, or Stage IV melanoma in combination with ipilimumab for the treatment of MSI-H or dMMR unresectable and metastatic CRC, and as a single agent for the treatment of MSI-H or dMMR mCRC that has progressed following treatment with a fluoropyrimidine, oxaliplatin, and irinotecan. Use of OPDIVO for these indications is supported by evidence from adequate and well-controlled studies in adults with melanoma or MSI-H or dMMR mCRC and additional pharmacokinetic data in pediatric patients. Nivolumab exposure in pediatric patients 12 years and older is comparable to that of adults and the courses of melanoma and MSI-H or dMMR mCRC are similar in pediatric patients aged 12 years and older to that of adults to allow extrapolation of safety and efficacy [see Adverse Reactions (6.1), Clinical Pharmacology (12.3), Clinical Studies (14.1, 14.11)].

The safety and effectiveness of OPDIVO have not been established for pediatric patients younger than 12 years old with melanoma or MSI-H or dMMR mCRC.

The safety and effectiveness of OPDIVO have not been established in pediatric patients with non-small cell lung cancer, malignant pleural mesothelioma, advanced renal cell carcinoma, classical Hodgkin lymphoma, squamous cell carcinoma of the head and neck, urothelial carcinoma, hepatocellular carcinoma, esophageal cancer, gastric cancer, gastroesophageal cancer and esophageal adenocarcinoma.

8.5 Geriatric Use

Single Agent

Of 3569 patients with melanoma, NSCLC, renal cell carcinoma, urothelial carcinoma, ESCC, and esophageal or gastroesophageal junction cancer who were randomized to single agent OPDIVO in clinical studies, 41% were 65 years and over and 10% were 75 years and over. No overall differences in safety or effectiveness were observed between elderly patients and younger patients [see Clinical Studies (14.1, 14.2, 14.5, 14.7, 14.10, 14.13, 14.14)].

In patients with cHL, recurrent head and neck SCC, or dMMR or MSI-H metastatic CRC (mCRC) who were treated with single agent OPDIVO in clinical studies did not include sufficient numbers of patients aged 65 years and over to determine whether they respond differently from younger patients [see Clinical Studies (14.8, 14.9, 14.11)].

OPDIVO in Combination with Ipilimumab

Of the 314 patients with melanoma who were randomized to OPDIVO in combination with ipilimumab, 41% were 65 years or older and 11% were 75 years or older. No overall differences in safety or effectiveness were reported between elderly patients and younger patients [see Clinical Studies (14.1)].

Of the 576 patients with NSCLC who were randomized to OPDIVO in combination with ipilimumab, 48% were 65 years or older and 10% were 75 years or older. No overall difference in safety was reported between older patients and younger patients; however, there was a higher discontinuation rate due to adverse reactions in patients aged 75 years or older (29%) relative to all patients who received OPDIVO with ipilimumab (18%). Of the 396 patients in the primary efficacy population (PD-L1 ≥1%) randomized to OPDIVO in combination with ipilimumab, the hazard ratio for overall survival was 0.70 (95% CI: 0.55, 0.89) in the 199 patients younger than 65 years compared to 0.91 (95% CI: 0.72, 1.15) in the 197 patients 65 years or older [see Clinical Studies (14.3)].

Of the 303 patients with malignant pleural mesothelioma who were randomized to OPDIVO in combination with ipilimumab, 77% were 65 years old or older and 26% were 75 years or older. No overall difference in safety was reported between older patients and younger patients; however, there were higher rates of serious adverse reactions and discontinuation due to adverse reactions in patients aged 75 years or older (68% and 35%, respectively) relative to all patients who received OPDIVO with ipilimumab (54% and 28%, respectively). For patients aged 75 years or older who received chemotherapy, the rate of serious adverse reactions was 34% and the discontinuation rate due to adverse reactions was 26% relative to 28% and 19% respectively for all patients. The hazard ratio for overall survival was 0.76 (95% CI: 0.52, 1.11) in the 71 patients younger than 65 years compared to 0.74 (95% CI: 0.59, 0.93) in the 232 patients 65 years or older randomized to OPDIVO in combination with ipilimumab [see Clinical Studies (14.6)].

Of the 550 patients with renal cell carcinoma who were randomized to OPDIVO in combination with ipilimumab, 38% were 65 years or older and 8% were 75 years or older. No overall difference in safety was reported between elderly patients and younger patients. In elderly patients with intermediate or poor risk, no overall difference in effectiveness was reported [see Clinical Studies (14.7)].

Of the 354 patients with dMMR or MSI-H metastatic CRC (mCRC) who were randomized to OPDIVO in combination with ipilimumab, 44% were 65 years or older and 14% were 75 years or older. Of the 353 patients randomized to OPDIVO, as a single agent, 45% were 65 years or older and 13% were 75 years or older. There was a higher incidence of any Grade 3 or 4 adverse reactions (55%) in patients aged 65 years or older receiving OPDIVO in combination with ipilimumab compared to those younger than 65 receiving the combination (42%). There was also a higher incidence of any Grade 3 or 4 adverse reactions (55%) in patients aged 65 years or older receiving OPDIVO in combination with ipilimumab relative to patients aged 65 years or older receiving single-agent OPDIVO (41%). There was a similar incidence of any Grade 3 or 4 adverse reactions in patients receiving single-agent OPDIVO aged 65 years or older (41%) relative to patients younger than 65 years (45%). Patients 65 years or older who received OPDIVO with ipilimumab discontinued treatment due to adverse reaction at a higher rate (23%) relative to patients 65 years or older receiving nivolumab (15%). No overall differences in effectiveness were reported between elderly patients and younger patients receiving either OPDIVO in combination with ipilimumab or single-agent OPDIVO [see Clinical Studies (14.11)].

Of the 335 patients with unresectable hepatocellular carcinoma who were randomized to OPDIVO in combination with ipilimumab, 52% were 65 years or older and 14% were 75 years or older. No overall difference in safety was reported between elderly patients and younger patients, however, there were higher rates of serious adverse reactions and discontinuation due to adverse reactions in patients aged 75 years or older (67% and 35%, respectively) relative to all patients who received OPDIVO with ipilimumab (53% and 27%, respectively).

Of the 49 patients with hepatocellular carcinoma who were treated with OPDIVO in combination with ipilimumab, 29% were between 65 years and 74 years of age and 8% were 75 years or older. Clinical studies of OPDIVO in combination with ipilimumab did not include sufficient numbers of patients with hepatocellular carcinoma aged 65 and over to determine whether they respond differently from younger patients [see Clinical Studies (14.12)].

Of the 325 patients with ESCC who were randomized to OPDIVO in combination with ipilimumab, 43% were 65 years old or older and 7% were 75 years or older. No overall difference in safety was reported between older patients and younger patients; however, there was a higher discontinuation rate due to adverse reactions in patients aged 75 years or older (38%) relative to all patients who received OPDIVO with ipilimumab (23%). For patients aged 75 years or older who received chemotherapy, the discontinuation rate due to adverse reactions was 33% relative to 23% for all patients [see Clinical Studies (14.13)].

OPDIVO in Combination with Platinum-Containing Chemotherapy

Of the 179 patients with NSCLC who were randomized to OPDIVO in combination with platinum-doublet chemotherapy, 48% were 65 years old or older and 6% were 75 years old or older. No overall differences in safety or effectiveness were reported between patients older and younger than 65 years [see Clinical Studies (14.3)].

Of the 229 patients with NSCLC who were randomized to OPDIVO 360 mg in combination with platinum-doublet chemotherapy every 3 weeks for up to 4 cycles, followed by OPDIVO 480 mg every 4 weeks, 56% were 65 years old or older and 7% were 75 years old or older. No overall differences in safety or effectiveness were reported between patients older and younger than 65 years.

Of the 1,110 patients with ESCC, GC, GEJC, or EAC who were randomized to OPDIVO in combination with fluoropyrimidine- and platinum-containing chemotherapy, 42% were 65 years or older and 10% were 75 years or older. No overall difference in safety was reported between elderly patients and younger patients [see Clinical Studies (14.13, 14.14)].

Of the 304 patients with UC who were treated with OPDIVO in combination with gemcitabine and platinum-doublet chemotherapy, 40% were 65 years or older and 11% were 75 years or older. No overall differences in safety or effectiveness were observed between patients 65 years of age and over and younger patients. Clinical studies of OPDIVO with platinum-doublet chemotherapy did not include sufficient numbers of patients aged 75 years and over to determine whether safety and effectiveness differs compared to younger patients. [see Clinical Studies (14.10)].

OPDIVO in Combination with Ipilimumab and Platinum-Doublet Chemotherapy

Of the 361 patients with NSCLC who were randomized to OPDIVO in combination with ipilimumab and platinum-doublet chemotherapy, 51% were 65 years or older and 10% were 75 years or older. No overall difference in safety was reported between older patients and younger patients; however, there was a higher discontinuation rate due to adverse reactions in patients aged 75 years or older (43%) relative to all patients who received OPDIVO with ipilimumab and chemotherapy (24%). For patients aged 75 years or older who received chemotherapy only, the discontinuation rate due to adverse reactions was 16% relative to all patients who had a discontinuation rate of 13%. Based on an updated analysis for overall survival, of the 361 patients randomized to OPDIVO in combination with ipilimumab and platinum-doublet chemotherapy, the hazard ratio for overall survival was 0.61 (95% CI: 0.47, 0.80) in the 176 patients younger than 65 years compared to 0.73 (95% CI: 0.56, 0.95) in the 185 patients 65 years or older [see Clinical Studies (14.5)].

OPDIVO in Combination with Cabozantinib

Of the 320 patients with renal cell carcinoma who were treated with OPDIVO in combination with cabozantinib, 41% were 65 years or older and 9% were 75 years or older. No overall difference in safety was reported between elderly patients and younger patients [see Clinical Studies (14.7)].

11 DESCRIPTION

Nivolumab is a programmed death receptor-1 (PD-1) blocking antibody. Nivolumab is an IgG4 kappa immunoglobulin that has a calculated molecular mass of 146 kDa. It is expressed in a recombinant Chinese Hamster Ovary (CHO) cell line.

OPDIVO is a sterile, preservative-free, non-pyrogenic, clear to opalescent, colorless to pale-yellow liquid that may contain light (few) particles.

OPDIVO (nivolumab) injection for intravenous use is supplied in single-dose vials. Each mL of OPDIVO solution contains nivolumab 10 mg, mannitol (30 mg), pentetic acid (0.008 mg), polysorbate 80 (0.2 mg), sodium chloride (2.92 mg), sodium citrate dihydrate (5.88 mg), and Water for Injection, USP. May contain hydrochloric acid and/or sodium hydroxide to adjust pH to 6.

12 CLINICAL PHARMACOLOGY

12.1 Mechanism of Action

Binding of the PD-1 ligands, PD-L1 and PD-L2, to the PD-1 receptor found on T cells, inhibits T-cell proliferation and cytokine production. Upregulation of PD-1 ligands occurs in some tumors and signaling through this pathway can contribute to inhibition of active T-cell immune surveillance of tumors. Nivolumab is a human immunoglobulin G4 (IgG4) monoclonal antibody that binds to the PD-1 receptor and blocks its interaction with PD-L1 and PD-L2, releasing PD-1 pathway-mediated inhibition of the immune response, including the anti-tumor immune response. In syngeneic mouse tumor models, blocking PD-1 activity resulted in decreased tumor growth.

Combined nivolumab (anti-PD-1) and ipilimumab (anti-CTLA-4) mediated inhibition results in enhanced T-cell function that is greater than the effects of either antibody alone, and results in improved anti-tumor responses in metastatic melanoma and advanced RCC. In murine syngeneic tumor models, dual blockade of PD-1 and CTLA-4 resulted in increased anti-tumor activity.

12.2 Pharmacodynamics

There are no clinically significant exposure-response relationships for efficacy or safety for nivolumab monotherapy across the approved dosing regimens, regardless of cancer type.

12.3 Pharmacokinetics

Nivolumab pharmacokinetics (PK) was assessed using a population PK approach for both single agent OPDIVO and OPDIVO with ipilimumab. The PK of nivolumab was studied in patients over a dose range of 0.1 mg/kg to 20 mg/kg administered as a single dose or as multiple doses of OPDIVO as a 60-minute intravenous infusion every 2 or 3 weeks. The exposure to nivolumab increases dose proportionally over the dose range of 0.1 to 10 mg/kg administered every 2 weeks. The predicted exposure of nivolumab after a 30-minute infusion is comparable to that observed with a 60-minute infusion. Steady-state concentrations of nivolumab were reached by 12 weeks when administered at 3 mg/kg every 2 weeks, and systemic accumulation was 3.7-fold.

Distribution

The geometric mean volume of distribution at steady state (Vss) and coefficient of variation (CV%) is 6.8 L (27.3%).

Elimination

Nivolumab clearance (CL) decreases over time, with a mean maximal reduction from baseline values (CV%) of 24.5% (47.6%) resulting in a geometric mean steady-state clearance (CLss) (CV%) of 8.2 mL/h (53.9%) in patients with metastatic tumors; the decrease in CLss is not considered clinically relevant. Nivolumab clearance does not decrease over time in patients with completely resected melanoma, as the geometric mean population clearance is 24% lower in this patient population compared with patients with metastatic melanoma at steady state.

The geometric mean elimination half-life (t1/2) is 25 days (77.5%).

Specific Populations

The following factors had no clinically important effect on the clearance of nivolumab: age (29 to 87 years), weight (35 to 160 kg), sex, race, baseline LDH, PD-L1 expression, solid tumor type, tumor size, renal impairment (eGFR ≥ 15 mL/min/1.73 m^2), and mild (total bilirubin [TB] less than or equal to the ULN and AST greater than ULN or TB greater than 1 to 1.5 times ULN and any AST) or moderate hepatic impairment (TB greater than 1.5 to 3 times ULN and any AST). Nivolumab has not been studied in patients with severe hepatic impairment (TB greater than 3 times ULN and any AST).

Pediatric Patients

The exposures of nivolumab, as monotherapy or in combination with ipilimumab, in pediatric patients 12 years of age or older are within range of those in adults at the recommended dosage [see Dosage and Administration (2.2)].

Drug Interaction Studies

When OPDIVO 3 mg/kg every 3 weeks was administered in combination with ipilimumab 1 mg/kg every 3 weeks, the CL of nivolumab and ipilimumab were unchanged compared to nivolumab or ipilimumab administered alone.

When OPDIVO 1 mg/kg every 3 weeks was administered in combination with ipilimumab 3 mg/kg every 3 weeks, the CL of nivolumab was increased by 29% compared to OPDIVO administered alone and the CL of ipilimumab was unchanged compared to ipilimumab administered alone.

When OPDIVO 3 mg/kg every 2 weeks was administered in combination with ipilimumab 1 mg/kg every 6 weeks, the CL of nivolumab was unchanged compared to OPDIVO administered alone and the CL of ipilimumab was increased by 30% compared to ipilimumab administered alone.

When OPDIVO 360 mg every 3 weeks was administered in combination with ipilimumab 1 mg/kg every 6 weeks and chemotherapy, the CL of nivolumab was unchanged compared to OPDIVO administered alone and the CL of ipilimumab increased by 22% compared to ipilimumab administered alone.

12.6 Immunogenicity

The observed incidence of anti-drug antibodies is highly dependent on the sensitivity and specificity of the assay. Differences in assay methods preclude meaningful comparisons of the incidence of anti-drug antibodies in the studies described below with the incidence of anti-drug antibodies in other studies, including those of OPDIVO or of other nivolumab products.

Anti-drug antibody and neutralizing antibody responses were monitored throughout the treatment period where the benefit to risk ratio was assessed. Incidence of anti-drug antibodies and neutralizing antibodies are presented in Table 55.

Table 55: OPDIVO Anti-Drug Antibody (ADA) and Neutralizing Antibody (NAb) Incidence
Treatment Regimena | Indication(s) | ADA | NAbb
OPDIVO as a single agent | Multiplec | 11% (229/2,085) | 7% (15/229)
OPDIVO with ipilimumab for 4 doses followed by OPDIVO as a single agent | Melanoma | 38% (149/394) | 12% (18/149)
OPDIVO with ipilimumab for 4 doses followed by OPDIVO as a single agent | HCC | 56% (27/48) | 41% (11/27)
OPDIVO with ipilimumab for 4 doses followed by OPDIVO as a single agent | RCC and CRC | 26% (132/516) | 3% (4/132)
OPDIVO with ipilimumab | Malignant Pleural Mesothelioma | 26% (69/269) | 2.9% (2/69)
OPDIVO with ipilimumab | NSCLC | 37% (180/491) | 3.9% (7/180)
OPDIVO with ipilimumab and 2 cycles of platinum‑doublet chemotherapy | NSCLC | 34% (104/308) | 8% (8/104)
a Details of each treatment regimen are described in Section 14 [see Clinical Studies (14)].
b NAb incidence is reported among the subset of patients positive for ADA.
c Includes unresectable or metastatic melanoma, metastatic NSCLC, advanced RCC, cHL, recurrent or metastatic SCCHN, and UC indications.
ADA = treatment-emergent anti-nivolumab antibodies, NAb = neutralizing antibodies, HCC = hepatocellular carcinoma, RCC = renal cell carcinoma, CRC = colorectal cancer, NSCLC = non-small cell lung cancer.

Effects of Anti-Drug Antibodies

Presence of treatment-emergent anti-nivolumab antibodies increased nivolumab clearance by up to 20% after administration of nivolumab as monotherapy or in combination with ipilimumab. These anti-drug antibody-associated pharmacokinetic changes were not considered to be clinically significant. There was no identified clinically significant effect of anti-drug antibodies on incidence of infusion-related reactions. The effects of anti-drug antibodies on effectiveness have not been fully characterized.

13 NONCLINICAL TOXICOLOGY

13.1 Carcinogenesis, Mutagenesis, Impairment of Fertility

No studies have been performed to assess the potential of nivolumab for carcinogenicity or genotoxicity. Fertility studies have not been performed with nivolumab. In 1-month and 3-month repeat-dose toxicology studies in monkeys, there were no notable effects in the male and female reproductive organs; however, most animals in these studies were not sexually mature.

13.2 Animal Toxicology and/or Pharmacology

In animal models, inhibition of PD-1 signaling increased the severity of some infections and enhanced inflammatory responses. M. tuberculosis–infected PD-1 knockout mice exhibit markedly decreased survival compared with wild-type controls, which correlated with increased bacterial proliferation and inflammatory responses in these animals. PD-1 knockout mice have also shown decreased survival following infection with lymphocytic choriomeningitis virus.

14 CLINICAL STUDIES

14.1 Unresectable or Metastatic Melanoma

Previously Treated Metastatic Melanoma

CHECKMATE-037 (NCT01721746) was a multicenter, open-label trial that randomized (2:1) patients with unresectable or metastatic melanoma to receive OPDIVO 3 mg/kg intravenously every 2 weeks or investigator’s choice of chemotherapy, either single-agent dacarbazine 1000 mg/m^2 every 3 weeks or the combination of carboplatin AUC 6 intravenously every 3 weeks and paclitaxel 175 mg/m^2 intravenously every 3 weeks. Patients were required to have progression of disease on or following ipilimumab treatment and, if BRAF V600 mutation positive, a BRAF inhibitor. The trial excluded patients with autoimmune disease, medical conditions requiring systemic immunosuppression, ocular melanoma, active brain metastasis, or a history of Grade 4 ipilimumab-related adverse reactions (except for endocrinopathies) or Grade 3 ipilimumab-related adverse reactions that had not resolved or were inadequately controlled within 12 weeks of the initiating event. Tumor assessments were conducted 9 weeks after randomization then every 6 weeks for the first year, and every 12 weeks thereafter.

Efficacy was evaluated in a single-arm, non-comparative, planned interim analysis of the first 120 patients who received OPDIVO in CHECKMATE-037 and in whom the minimum duration of follow-up was 6 months. The major efficacy outcome measures in this population were confirmed overall response rate (ORR) as measured by blinded independent central review using Response Evaluation Criteria in Solid Tumors (RECIST 1.1) and duration of response.

Among the 120 patients treated with OPDIVO, the median age was 58 years (range: 25 to 88), 65% of patients were male, 98% were White, and the ECOG performance score was 0 (58%) or 1 (42%). Disease characteristics were M1c disease (76%), BRAF V600 mutation positive (22%), elevated LDH (56%), history of brain metastases (18%), and two or more prior systemic therapies for metastatic disease (68%).

The ORR was 32% (95% confidence interval [CI]: 23, 41), consisting of 4 complete responses and 34 partial responses in OPDIVO-treated patients. Of 38 patients with responses, 87% had ongoing responses with durations ranging from 2.6+ to 10+ months, which included 13 patients with ongoing responses of 6 months or longer.

There were responses in patients with and without BRAF V600 mutation-positive melanoma. A total of 405 patients were randomized and the median duration of OS was 15.7 months (95% CI: 12.9, 19.9) in OPDIVO-treated patients compared to 14.4 months (95% CI: 11.7, 18.2) (HR 0.95; 95.54% CI: 0.73, 1.24) in patients assigned to investigator’s choice of treatment. Figure 1 summarizes the OS results.

Figure 1: Overall Survival - CHECKMATE-037*

* The primary OS analysis was not adjusted to account for subsequent therapies, with 54 (40.6%) patients in the chemotherapy arm subsequently receiving an anti-PD1 treatment. OS may be confounded by dropout, imbalance of subsequent therapies, and differences in baseline factors.

Previously Untreated Metastatic Melanoma

CHECKMATE-066

CHECKMATE-066 (NCT01721772) was a multicenter, double-blind, randomized (1:1) trial in 418 patients with BRAF V600 wild-type unresectable or metastatic melanoma. Patients were randomized to receive either OPDIVO 3 mg/kg by intravenous infusion every 2 weeks or dacarbazine 1000 mg/m^2 intravenously every 3 weeks until disease progression or unacceptable toxicity. Randomization was stratified by PD-L1 status (≥5% of tumor cell membrane staining by immunohistochemistry vs. <5% or indeterminate result) and M stage (M0/M1a/M1b versus M1c). Key eligibility criteria included histologically confirmed, unresectable or metastatic, cutaneous, mucosal, or acral melanoma; no prior therapy for metastatic disease; completion of prior adjuvant or neoadjuvant therapy at least 6 weeks prior to randomization; ECOG performance status 0 or 1; absence of autoimmune disease; and absence of active brain or leptomeningeal metastases. The trial excluded patients with ocular melanoma. Tumor assessments were conducted 9 weeks after randomization then every 6 weeks for the first year and then every 12 weeks thereafter. The major efficacy outcome measure was overall survival (OS). Additional outcome measures included investigator-assessed progression-free survival (PFS) and ORR per RECIST v1.1.

The trial population characteristics were: median age was 65 years (range: 18 to 87), 59% were male, and 99.5% were White. Disease characteristics were M1c stage disease (61%), cutaneous melanoma (74%), mucosal melanoma (11%), elevated LDH level (37%), PD-L1 ≥5% tumor cell membrane expression (35%), and history of brain metastasis (4%). More patients in the OPDIVO arm had an ECOG performance status of 0 (71% vs. 58%).

CHECKMATE-066 demonstrated a statistically significant improvement in OS for the OPDIVO arm compared with the dacarbazine arm in an interim analysis based on 47% of the total planned events for OS. At the time of analysis, 88% (63/72) of OPDIVO-treated patients had ongoing responses, which included 43 patients with ongoing response of 6 months or longer. Efficacy results are shown in Table 56 and Figure 2.

Table 56: Efficacy Results - CHECKMATE-066
 | OPDIVO (n=210) | Dacarbazine (n=208)
Overall Survival
Deaths (%) | 50 (24) | 96 (46)
Median (months) (95% CI) | NRa | 10.8 (9.3, 12.1)
Hazard ratio (95% CI)b | 0.42 (0.30, 0.60)
p-valuec,d | <0.0001
Progression-free Survival
Disease progression or death (%) | 108 (51) | 163 (78)
Median (months) (95% CI) | 5.1 (3.5, 10.8) | 2.2 (2.1, 2.4)
Hazard ratio (95% CI)b | 0.43 (0.34, 0.56)
p-valuec,d | <0.0001
Overall Response Rate | 34% | 9%
(95% CI) | (28, 41) | (5, 13)
Complete response rate | 4% | 1%
Partial response rate | 30% | 8%
a Not Reached.
b Based on a stratified proportional hazards model.
c Based on stratified log-rank test.
d p-value is compared with the allocated alpha of 0.0021 for this interim analysis.

Figure 2: Overall Survival - CHECKMATE-066

CHECKMATE-067

CHECKMATE-067 (NCT01844505) was a multicenter, randomized (1:1:1), double-blind trial in 945 patients with previously untreated, unresectable or metastatic melanoma to one of the following arms: OPDIVO and ipilimumab, OPDIVO, or ipilimumab. Patients were required to have completed adjuvant or neoadjuvant treatment at least 6 weeks prior to randomization and have no prior treatment with anti-CTLA-4 antibody and no evidence of active brain metastasis, ocular melanoma, autoimmune disease, or medical conditions requiring systemic immunosuppression.

Patients were randomized to receive:

- OPDIVO 1 mg/kg with ipilimumab 3 mg/kg intravenously every 3 weeks for 4 doses, followed by OPDIVO as a single agent at a dose of 3 mg/kg by intravenous infusion every 2 weeks (OPDIVO and ipilimumab arm),
- OPDIVO 3 mg/kg by intravenous infusion every 2 weeks (OPDIVO arm), or
- Ipilimumab 3 mg/kg intravenously every 3 weeks for 4 doses, followed by placebo every 2 weeks (ipilimumab arm).

Randomization was stratified by PD-L1 expression (≥5% vs. <5% tumor cell membrane expression) as determined by a clinical trial assay, BRAF V600 mutation status, and M stage per the AJCC staging system (M0, M1a, M1b vs. M1c). Tumor assessments were conducted 12 weeks after randomization then every 6 weeks for the first year, and every 12 weeks thereafter. The major efficacy outcome measures were investigator-assessed PFS per RECIST v1.1 and OS. Additional efficacy outcome measures were confirmed ORR and duration of response.

The trial population characteristics were: median age 61 years (range: 18 to 90); 65% male; 97% White; ECOG performance score 0 (73%) or 1 (27%). Disease characteristics were: AJCC Stage IV disease (93%); M1c disease (58%); elevated LDH (36%); history of brain metastases (4%); BRAF V600 mutation-positive melanoma (32%); PD-L1 ≥5% tumor cell membrane expression as determined by the clinical trials assay (46%); and prior adjuvant therapy (22%).

CHECKMATE-067 demonstrated statistically significant improvements in OS and PFS for patients randomized to either OPDIVO-containing arm as compared with the ipilimumab arm. The trial was not designed to assess whether adding ipilimumab to OPDIVO improves PFS or OS compared to OPDIVO as a single agent. Efficacy results are shown in Table 57 and Figure 3.

Table 57: Efficacy Results - CHECKMATE-067
 | OPDIVO and Ipilimumab (n=314) | OPDIVO (n=316) | Ipilimumab (n=315)
Overall Survivala
Deaths (%) | 128 (41) | 142 (45) | 197 (63)
Hazard ratiob (vs. ipilimumab) (95% CI) | 0.55 (0.44, 0.69) | 0.63 (0.50, 0.78)
p-valuec, d | <0.0001 | <0.0001
Progression-free Survivala
Disease progression or death | 151 (48%) | 174 (55%) | 234 (74%)
Median (months) (95% CI) | 11.5 (8.9, 16.7) | 6.9 (4.3, 9.5) | 2.9 (2.8, 3.4)
Hazard ratiob (vs. ipilimumab) (95% CI) | 0.42 (0.34, 0.51) | 0.57 (0.47, 0.69)
p-valuec, e | <0.0001 | <0.0001
Confirmed Overall Response Ratea | 50% | 40% | 14%
(95% CI) | (44, 55) | (34, 46) | (10, 18)
p-valuef | <0.0001 | <0.0001
Complete response | 8.9% | 8.5% | 1.9%
Partial response | 41% | 31% | 12%
Duration of Response
Proportion ≥6 months in duration | 76% | 74% | 63%
Range (months) | 1.2+ to 15.8+ | 1.3+ to 14.6+ | 1.0+ to 13.8+
a OS results are based on final OS analysis with 28 months of minimum follow-up; PFS (co-primary endpoint) and ORR (secondary endpoint) results were based on primary analysis with 9 months of minimum follow-up.
b Based on a stratified proportional hazards model.
c Based on stratified log-rank test.
d If the maximum of the two OS p-values is less than 0.04 (a significance level assigned by the Hochberg procedure), then both p-values are considered significant.
e p-value is compared with .005 of the allocated alpha for final PFS treatment comparisons.
f Based on the stratified Cochran-Mantel-Haenszel test.
+ Censored observation

Figure 3: Overall Survival - CHECKMATE-067

Based on a minimum follow-up of 48 months, the median OS was not reached (95% CI: 38.2, NR) in the OPDIVO and ipilimumab arm. The median OS was 36.9 months (95% CI: 28.3, NR) in the OPDIVO arm and 19.9 months (95% CI: 16.9, 24.6) in the ipilimumab arm.

Based on a minimum follow-up of 28 months, the median PFS was 11.7 months (95% CI: 8.9, 21.9) in the OPDIVO and ipilimumab arm, 6.9 months (95% CI: 4.3, 9.5) in the OPDIVO arm, and 2.9 months (95% CI: 2.8, 3.2) in the ipilimumab arm. Based on a minimum follow-up of 28 months, the proportion of responses lasting ≥24 months was 55% in the OPDIVO and ipilimumab arm, 56% in the OPDIVO arm, and 39% in the ipilimumab arm.

14.2 Adjuvant Treatment of Melanoma

CHECKMATE-76K

CHECKMATE-76K (NCT04099251) was a randomized, double-blind trial in 790 patients with completely resected Stage IIB/C melanoma. Patients were randomized (2:1) to receive OPDIVO 480 mg or placebo by intravenous infusion every 4 weeks for up to 1 year or until disease recurrence or unacceptable toxicity. Enrollment required complete resection of the primary melanoma with negative margins and a negative sentinel lymph node within 12 weeks prior to randomization, and ECOG performance status of 0 or 1. The trial excluded patients with ocular/uveal or mucosal melanoma, autoimmune disease, any condition requiring systemic treatment with either corticosteroids (≥10 mg daily prednisone or equivalent) or other immunosuppressive medications, as well as patients with prior therapy for melanoma except surgery. Randomization was stratified by AJCC 8th staging system edition (T3b vs. T4a vs. T4b). The major efficacy outcome measure was recurrence-free survival (RFS) defined as the time between the date of randomization and the date of first recurrence (local, regional, or distant metastasis), new primary melanoma, or death, from any cause, whichever occurred first and as assessed by the investigator. Tumor assessments were conducted every 26 weeks during years 1-3 and every 52 weeks thereafter until year 5.

The trial population characteristics were: median age 62 years (range: 19 to 92), 61% were male, 98% were White, 0.4% Black or African American, 0.1% Asian, and 1.1% race unknown, 2.2% Hispanic or Latino, 58% Not Hispanic or Latino, 40% ethnicity unknown, and 94% had an ECOG performance status of 0. Sixty one percent had stage IIB and 39% had stage IIC melanoma.

CHECKMATE-76K demonstrated a statistically significant improvement in RFS for patients randomized to the OPDIVO arm compared with the placebo arm. Efficacy results are shown in Table 58 and Figure 4.

Table 58: Efficacy Results - CHECKMATE-76K
 | OPDIVO n=526 | Placebo n=264
Recurrence-free Survival
Number of events, n (%) | 66 (13%) | 69 (26%)
Median (months)b (95% CI) | NRa (28.5, NR) | NRa (21.6, NR)
Hazard ratioc (95% CI) p-valued | 0.42 (0.30, 0.59) p<0.0001
a Not reached.
b Based on Kaplan-Meier estimates.
c Hazard Ratio is OPDIVO over placebo based on a stratified Cox proportional hazard model.
d Based on a 2-sided stratified log-rank test. Boundary for statistical significance: p‑value <0.033.

Figure 4: Recurrence-free Survival - CHECKMATE-76K

CHECKMATE-238

CHECKMATE-238 (NCT02388906) was a randomized, double-blind trial in 906 patients with completely resected Stage IIIB/C or Stage IV melanoma. Patients were randomized (1:1) to receive OPDIVO 3 mg/kg by intravenous infusion every 2 weeks or ipilimumab 10 mg/kg intravenously every 3 weeks for 4 doses then every 12 weeks beginning at Week 24 for up to 1 year. Enrollment required complete resection of melanoma with margins negative for disease within 12 weeks prior to randomization. The trial excluded patients with a history of ocular/uveal melanoma, autoimmune disease, and any condition requiring systemic treatment with either corticosteroids (≥10 mg daily prednisone or equivalent) or other immunosuppressive medications, as well as patients with prior therapy for melanoma except surgery, adjuvant radiotherapy after neurosurgical resection for lesions of the central nervous system, and prior adjuvant interferon completed ≥6 months prior to randomization. Randomization was stratified by PD-L1 status (positive [based on 5% level] vs. negative/indeterminate) and AJCC stage (Stage IIIB/C vs. Stage IV M1a-M1b vs. Stage IV M1c). The major efficacy outcome measure was recurrence-free survival (RFS) defined as the time between the date of randomization and the date of first recurrence (local, regional, or distant metastasis), new primary melanoma, or death, from any cause, whichever occurs first and as assessed by the investigator. Patients underwent imaging for tumor recurrence every 12 weeks for the first 2 years then every 6 months thereafter.

The trial population characteristics were: median age was 55 years (range: 18 to 86), 58% were male, 95% were White, and 90% had an ECOG performance status of 0. Disease characteristics were AJCC Stage IIIB (34%), Stage IIIC (47%), Stage IV (19%), M1a-b (14%), BRAF V600 mutation positive (42%), BRAF wild-type (45%), elevated LDH (8%), PD-L1 ≥5% tumor cell membrane expression determined by clinical trial assay (34%), macroscopic lymph nodes (48%), and tumor ulceration (32%).

CHECKMATE-238 demonstrated a statistically significant improvement in RFS for patients randomized to the OPDIVO arm compared with the ipilimumab 10 mg/kg arm. Efficacy results are shown in Table 59 and Figure 5.

Table 59: Efficacy Results - CHECKMATE-238
 | OPDIVO N=453 | Ipilimumab 10 mg/kg N=453
Recurrence-free Survival
Number of events, n (%) | 154 (34%) | 206 (45%)
Median (months) (95% CI) | NRa | NRa (16.56, NRa)
Hazard ratiob (95% CI) p-valuec,d | 0.65 (0.53, 0.80) p<0.0001
Overall Survival
Number of events, n (%)e | 100 (22%) | 111 (25%)
Median (months) (95% CI) | NRa | NRa
Hazard ratiob (95% CI) p-value | 0.87 (0.67, 1.14) 0.3148
a Not reached.
b Based on a stratified proportional hazards model.
c Based on a stratified log-rank test.
d p-value is compared with 0.0244 of the allocated alpha for this analysis.
e At the time of the final OS analysis, fewer overall survival events were observed than originally anticipated (approximately 302).

Figure 5: Recurrence-free Survival - CHECKMATE-238

14.3 Neoadjuvant Treatment of Resectable (Tumors ≥4 cm or Node Positive) Non-Small Cell Lung Cancer

CHECKMATE-816 (NCT02998528) was a randomized, open label trial in patients with resectable NSCLC. The trial included patients with resectable, histologically confirmed Stage IB (≥4 cm), II, or IIIA NSCLC (per the 7th edition American Joint Committee on Cancer/Union for International Cancer Control (AJCC/UICC) staging criteria), ECOG performance status 0 or 1, and measurable disease (per RECIST version 1.1). Patients with unresectable or metastatic NSCLC, known EGFR mutations or ALK translocations, Grade 2 or greater peripheral neuropathy, active autoimmune disease, or medical conditions requiring systemic immunosuppression were excluded from the study.

Patients were randomized to receive either:

- OPDIVO 360 mg administered intravenously over 30 minutes and platinum-doublet chemotherapy administered intravenously every 3 weeks for up to 3 cycles, or
- platinum-doublet chemotherapy administered every 3 weeks for up to 3 cycles.

Platinum-doublet chemotherapy consisted of paclitaxel 175 mg/m^2 or 200 mg/m^2 and carboplatin AUC 5 or AUC 6 (any histology); pemetrexed 500 mg/m^2 and cisplatin 75 mg/m^2 (non-squamous histology); or gemcitabine 1000 mg/m^2 or 1250 mg/m^2 and cisplatin 75 mg/m^2 (squamous histology). In the platinum-doublet chemotherapy arm, two additional treatment regimen options included vinorelbine 25 mg/m^2 or 30 mg/m^2 and cisplatin 75 mg/m^2; or docetaxel 60 mg/m^2 or 75 mg/m^2 and cisplatin 75 mg/m^2 (any histology).

Stratification factors for randomization were tumor PD-L1 expression level (≥1% versus <1% or non-quantifiable), disease stage (IB/II versus IIIA), and sex (male versus female). Tumor assessments were performed at baseline, within 14 days of surgery, every 12 weeks after surgery for 2 years, then every 6 months for 3 years, and every year for 5 years until disease recurrence or progression. The major efficacy outcome measures were event-free survival (EFS) based on blinded independent central review (BICR) assessment and pathologic complete response (pCR) as evaluated by blinded independent pathology review (BIPR). Additional efficacy outcome measures included OS.

A total of 358 patients were randomized to receive either OPDIVO in combination with platinum-doublet chemotherapy (n=179) or platinum-doublet chemotherapy (n=179). The median age was 65 years (range: 34 to 84) with 51% of patients ≥65 years and 7% of patients ≥75 years, 50% were Asian, 47% were White, 2% were Black, and 71% were male. Baseline ECOG performance status was 0 (67%) or 1 (33%); 50% had tumors with PD-L1 expression ≥1%; 35% had stage IB/II and 64% had stage IIIA disease; 51% had tumors with squamous histology and 49% had tumors with non-squamous histology; and 89% were former/current smokers.

Eighty-three percent of patients in the OPDIVO in combination with platinum-doublet chemotherapy arm had definitive surgery compared to 75% of patients in the platinum-doublet chemotherapy arm.

The study demonstrated statistically significant improvements in EFS and pCR. Efficacy results are presented in Table 60 and Figure 6.

Table 60: Efficacy Results - CHECKMATE-816
 | OPDIVO and Platinum-Doublet Chemotherapy (n=179) | Platinum-Doublet Chemotherapy (n=179)
Event-free Survival (EFS) per BICR
Events (%) | 64 (35.8) | 87 (48.6)
Median (months)a; (95% CI) | 31.6; (30.2, NR) | 20.8; (14.0, 26.7)
Hazard Ratiob; (95% CI) | 0.63; (0.45, 0.87)
Stratified log-rank p-valuec | 0.0052
Pathologic Complete Response (pCR) per BIPR
Number of patients with pCR | 43 | 4
pCR Rate (%), (95% CI)d | 24.0 (18.0, 31.0) | 2.2 (0.6, 5.6)
Estimated treatment difference (95% CI)e | 21.6 (15.1, 28.2)
p-valuef | <0.0001
Minimum follow-up for EFS was 21 months.
a Kaplan-Meier estimate.
b Based on a stratified Cox proportional hazard model.
c Based on a stratified log-rank test. Boundary for statistical significance: p-value <0.0262.
d Based on Clopper and Pearson method.
e Strata-adjusted difference based on Cochran-Mantel-Haenszel method of weighting.
f From stratified CMH test.

Figure 6: Event-Free Survival - CHECKMATE-816

At the time of the EFS analysis, 26% of the patients had died. A prespecified interim analysis for OS resulted in a HR of 0.57 (95% CI: 0.38, 0.87), which did not cross the boundary for statistical significance.

14.4 Neoadjuvant and Adjuvant Treatment of Resectable Non-Small Cell Lung Cancer

The efficacy of OPDIVO, in combination with platinum-doublet chemotherapy, followed by surgery, and continued adjuvant treatment with OPDIVO as a single agent, was investigated in CHECKMATE-77T (NCT04025879), a randomized, double-blind trial in 461 patients with resectable NSCLC. The trial included patients with resectable, suspected or histologically confirmed Stage IIA (>4 cm) to IIIB (T3-T4 N2) NSCLC (per the 8th edition American Joint Committee on Cancer (AJCC) Staging Manual), and ECOG performance status 0 or 1. Patients with unresectable or metastatic NSCLC, EGFR mutations or known ALK translocations, brain metastasis, Grade 2 or greater peripheral neuropathy, interstitial lung disease or active, non-infectious pneumonitis (symptomatic and/or requiring treatment), active autoimmune disease, or medical conditions requiring systemic immunosuppression were excluded from the study. Randomization was stratified by tumor PD-L1 expression level (≥1% versus <1% versus indeterminate/not evaluable), disease stage (Stage II versus Stage III), and tumor histology (squamous versus nonsquamous).

Patients were randomized (1:1) to receive either:

- Neoadjuvant OPDIVO 360 mg administered intravenously over 30 minutes in combination with one of the following platinum-doublet chemotherapy regimens every 3 weeks for four cycles:
  - Paclitaxel 175 mg/m^2 or 200 mg/m^2 and carboplatin AUC 5 or AUC 6 (any histology)
  - Pemetrexed 500 mg/m^2, and cisplatin 75 mg/m^2 or carboplatin AUC 5 or AUC 6 (nonsquamous histology)
  - Cisplatin 75 mg/m^2 and docetaxel 75 mg/m^2 (squamous histology).
Within 90 days after the surgery, OPDIVO 480 mg was administered intravenously over 30 minutes every 4 weeks.

or

- Neoadjuvant placebo administered intravenously over 30 minutes in combination with platinum-doublet chemotherapy (see above) every 3 weeks for four cycles. Within 90 days after the surgery, placebo was administered intravenously over 30 minutes every 4 weeks.

All study medications were administered via intravenous infusion. Treatment continued until disease progression, recurrence, or unacceptable toxicity for up to 13 cycles (1 year). Tumor assessments were performed every 12 weeks for 2 years, then every 24 weeks for up to 5 years or until disease recurrence or progression was confirmed by BICR.

The trial was not designed to isolate the effect of OPDIVO in each phase (neoadjuvant or adjuvant) of treatment.

The major efficacy outcome measure was event-free survival (EFS) based on BICR assessment. Additional efficacy outcome measures included overall survival (OS), pathologic complete response (pCR), and major pathologic response (MPR).

The median age was 66 years (range: 35 to 86); 71% were male; 72% were White, 25% were Asian, 1.7% were Black, and 1.5% were mixed race/ race unknown/ not reported; and 6% were Hispanic or Latino. Baseline ECOG performance status was 0 (62%) or 1 (38%); 56% had tumors with PD-L1 expression ≥1% and 40% had tumors with PD-L1 expression <1%; 35% had stage II and 64% had stage III disease; 23% had N1 disease and 39% had N2 disease; 51% had tumors with squamous histology and 49% had tumors with nonsquamous histology; and 90% were former/current smokers.

Seventy-eight percent of patients in the neoadjuvant OPDIVO in combination with platinum-doublet chemotherapy followed by adjuvant OPDIVO arm had definitive surgery compared to 77% of patients in the neoadjuvant placebo and platinum-doublet chemotherapy followed by placebo arm.

The study demonstrated a statistically significant improvement in EFS for patients treated with neoadjuvant OPDIVO in combination with platinum-doublet chemotherapy followed by single agent OPDIVO compared with patients randomized to placebo in combination with platinum-doublet chemotherapy followed by placebo. Efficacy results are presented in Table 61 and Figure 7.

Table 61: Efficacy Results - CHECKMATE-77T
 | Neoadjuvant OPDIVO and Platinum-Doublet Chemotherapy/Adjuvant OPDIVO; (n=229) | Neoadjuvant Placebo and Platinum-Doublet Chemotherapy/Adjuvant Placebo; (n=232)
Event-free Survival (EFS) per BICR
Events (%) | 76 (33%) | 113 (49%)
Median (months)a; (95% CI) | NR; (28.9, NR) | 18.4; (13.6, 28.1)
Hazard Ratiob; (95% CI) | 0.58; (0.43, 0.78)
Stratified log-rank p-valuec | 0.00025
a Kaplan-Meier estimate.
b Based on a stratified Cox proportional hazard model.
c Based on a stratified log-rank test. Boundary for statistical significance: p-value <0.0264.

Figure 7: Event-Free Survival - CHECKMATE-77T

In a pre-specified descriptive analysis, the pCR rate was 25% (95% CI: 20, 31) in the OPDIVO arm and 4.7% (95% CI: 2.4, 8) in the placebo arm.

At the time of the EFS analysis, OS data were immature.

14.5 Metastatic Non-Small Cell Lung Cancer

First-line Treatment of Metastatic Non-Small Cell Lung Cancer (NSCLC) Expressing PD-L1 (≥1%): In Combination with Ipilimumab

CHECKMATE-227 (NCT02477826) was a randomized, open-label, multi-part trial in patients with metastatic or recurrent NSCLC. The study included patients (18 years of age or older) with histologically confirmed Stage IV or recurrent NSCLC (per the 7th International Association for the Study of Lung Cancer [IASLC] classification), ECOG performance status 0 or 1, and no prior anticancer therapy. Patients were enrolled regardless of their tumor PD-L1 status. Patients with known EGFR mutations or ALK translocations sensitive to available targeted inhibitor therapy, untreated brain metastases, carcinomatous meningitis, active autoimmune disease, or medical conditions requiring systemic immunosuppression were excluded from the study. Patients with treated brain metastases were eligible if neurologically returned to baseline at least 2 weeks prior to enrolment, and either off corticosteroids, or on a stable or decreasing dose of <10 mg daily prednisone equivalents.

Primary efficacy results were based on Part 1a of the study, which was limited to patients with PD-L1 tumor expression ≥1%. Tumor specimens were evaluated prospectively using the PD-L1 IHC 28-8 pharmDx assay at a central laboratory. Randomization was stratified by tumor histology (non-squamous versus squamous). The evaluation of efficacy relied on the comparison between:

- OPDIVO 3 mg/kg administered intravenously over 30 minutes every 2 weeks in combination with ipilimumab 1 mg/kg administered intravenously over 30 minutes every 6 weeks; or
- Platinum-doublet chemotherapy

Chemotherapy regimens consisted of pemetrexed (500 mg/m^2) and cisplatin (75 mg/m^2) or pemetrexed (500 mg/m^2) and carboplatin (AUC 5 or 6) for non-squamous NSCLC or gemcitabine (1000 or 1250 mg/m^2) and cisplatin (75 mg/m^2) or gemcitabine (1000 mg/m^2) and carboplatin (AUC 5) (gemcitabine was administered on Days 1 and 8 of each cycle) for squamous NSCLC.

Study treatment continued until disease progression, unacceptable toxicity, or for up to 24 months. Treatment continued beyond disease progression if a patient was clinically stable and was considered to be deriving clinical benefit by the investigator. Patients who discontinued combination therapy because of an adverse event attributed to ipilimumab were permitted to continue OPDIVO as a single agent. Tumor assessments were performed every 6 weeks from the first dose of study treatment for the first 12 months, then every 12 weeks until disease progression or study treatment was discontinued. The primary efficacy outcome measure was OS. Additional efficacy outcome measures included PFS, ORR, and duration of response as assessed by BICR.

In Part 1a, a total of 793 patients were randomized to receive either OPDIVO in combination with ipilimumab (n=396) or platinum-doublet chemotherapy (n=397). The median age was 64 years (range: 26 to 87) with 49% of patients ≥65 years and 10% of patients ≥75 years, 76% White, and 65% male. Baseline ECOG performance status was 0 (34%) or 1 (65%), 50% with PD-L1 ≥50%, 29% with squamous and 71% with non-squamous histology, 10% had brain metastases, and 85% were former/current smokers.

The study demonstrated a statistically significant improvement in OS for PD-L1 ≥1% patients randomized to the OPDIVO and ipilimumab arm compared with the platinum-doublet chemotherapy arm. The OS results are presented in Table 62 and Figure 8.

Table 62: Efficacy Results (PD-L1 ≥1%) - CHECKMATE-227 Part 1a
 | OPDIVO and Ipilimumab (n=396) | Platinum-Doublet Chemotherapy (n=397)
Overall Survival
Events (%) | 258 (65%) | 298 (75%)
Median (months)a; (95% CI) | 17.1; (15, 20.1) | 14.9; (12.7, 16.7)
Hazard ratio (95% CI)b | 0.79 (0.67, 0.94)
Stratified log-rank p-value | 0.0066
a Kaplan-Meier estimate.
b Based on a stratified Cox proportional hazard model.

Figure 8: Overall Survival (PD-L1 ≥1%) - CHECKMATE-227

BICR-assessed PFS showed a HR of 0.82 (95% CI: 0.69, 0.97), with a median PFS of 5.1 months (95% CI: 4.1, 6.3) in the OPDIVO and ipilimumab arm and 5.6 months (95% CI: 4.6, 5.8) in the platinum-doublet chemotherapy arm. The BICR-assessed confirmed ORR was 36% (95% CI: 31, 41) in the OPDIVO and ipilimumab arm and 30% (95% CI: 26, 35) in the platinum-doublet chemotherapy arm. Median duration of response observed in the OPDIVO and ipilimumab arm was 23.2 months and 6.2 months in the platinum-doublet chemotherapy arm.

First-line Treatment of Metastatic or Recurrent NSCLC: In Combination with Ipilimumab and Platinum-Doublet Chemotherapy

CHECKMATE-9LA (NCT03215706) was a randomized, open-label trial in patients with metastatic or recurrent NSCLC. The trial included patients (18 years of age or older) with histologically confirmed Stage IV or recurrent NSCLC (per the 7th International Association for the Study of Lung Cancer classification [IASLC]), ECOG performance status 0 or 1, and no prior anticancer therapy (including EGFR and ALK inhibitors) for metastatic disease. Patients were enrolled regardless of their tumor PD-L1 status. Patients with known EGFR mutations or ALK translocations sensitive to available targeted inhibitor therapy, untreated brain metastases, carcinomatous meningitis, active autoimmune disease, or medical conditions requiring systemic immunosuppression were excluded from the study. Patients with stable brain metastases were eligible for enrollment.

Patients were randomized 1:1 to receive either:

- OPDIVO 360 mg administered intravenously over 30 minutes every 3 weeks, ipilimumab 1 mg/kg administered intravenously over 30 minutes every 6 weeks, and platinum-doublet chemotherapy administered intravenously every 3 weeks for 2 cycles, or
- platinum-doublet chemotherapy administered every 3 weeks for 4 cycles.

Platinum-doublet chemotherapy consisted of either carboplatin (AUC 5 or 6) and pemetrexed 500 mg/m^2, or cisplatin 75 mg/m^2 and pemetrexed 500 mg/m^2 for non-squamous NSCLC; or carboplatin (AUC 6) and paclitaxel 200 mg/m^2 for squamous NSCLC. Patients with non-squamous NSCLC in the control arm could receive optional pemetrexed maintenance therapy. Stratification factors for randomization were tumor PD-L1 expression level (≥1% versus <1% or non-quantifiable), histology (squamous versus non-squamous), and sex (male versus female). Study treatment continued until disease progression, unacceptable toxicity, or for up to 2 years. Treatment could continue beyond disease progression if a patient was clinically stable and was considered to be deriving clinical benefit by the investigator. Patients who discontinued combination therapy because of an adverse reaction attributed to ipilimumab were permitted to continue OPDIVO as a single agent as part of the study. Tumor assessments were performed every 6 weeks from the first dose of study treatment for the first 12 months, then every 12 weeks until disease progression or study treatment was discontinued. The primary efficacy outcome measure was OS. Additional efficacy outcome measures included PFS, ORR, and duration of response as assessed by BICR.

A total of 719 patients were randomized to receive either OPDIVO in combination with ipilimumab and platinum-doublet chemotherapy (n=361) or platinum-doublet chemotherapy (n=358). The median age was 65 years (range: 26 to 86) with 51% of patients ≥65 years and 10% of patients ≥75 years. The majority of patients were White (89%) and male (70%). Baseline ECOG performance status was 0 (31%) or 1 (68%), 57% had tumors with PD-L1 expression ≥1% and 37% had tumors with PD-L1 expression that was <1%, 32% had tumors with squamous histology and 68% had tumors with non-squamous histology, 17% had CNS metastases, and 86% were former or current smokers.

The study demonstrated a statistically significant benefit in OS, PFS, and ORR. Efficacy results from the prespecified interim analysis when 351 events were observed (87% of the planned number of events for final analysis) are presented in Table 63.

Table 63: Efficacy Results - CHECKMATE-9LA
 | OPDIVO and Ipilimumab and Platinum-Doublet Chemotherapy (n=361) | Platinum-Doublet Chemotherapy (n=358)
Overall Survival
Events (%) | 156 (43.2) | 195 (54.5)
Median (months); (95% CI) | 14.1 (13.2, 16.2) | 10.7 (9.5, 12.5)
Hazard ratio (96.71% CI)a | 0.69 (0.55, 0.87)
Stratified log-rank p-valueb | 0.0006
Progression-free Survival per BICR
Events (%) | 232 (64.3) | 249 (69.6)
Hazard ratio (97.48% CI)a | 0.70 (0.57, 0.86)
Stratified log-rank p-valuec | 0.0001
Median (months)d; (95% CI) | 6.8 (5.6, 7.7) | 5.0 (4.3, 5.6)
Overall Response Rate per BICR (%) | 38 | 25
(95% CI)e | (33, 43) | (21, 30)
Stratified CMH test p-valuef | 0.0003
Duration of Response per BICR
Median (months); (95% CI)d | 10.0 (8.2, 13.0) | 5.1 (4.3, 7.0)
a Based on a stratified Cox proportional hazard model.
b p-value is compared with the allocated alpha of 0.033 for this interim analysis.
c p-value is compared with the allocated alpha of 0.0252 for this interim analysis.
d Kaplan-Meier estimate.
e Confidence interval based on the Clopper and Pearson Method.
f p-value is compared with the allocated alpha of 0.025 for this interim analysis.

With an additional 4.6 months of follow-up, the hazard ratio for overall survival was 0.66 (95% CI: 0.55, 0.80) and median survival was 15.6 months (95% CI: 13.9, 20.0) and 10.9 months (95% CI: 9.5, 12.5) for patients receiving OPDIVO and ipilimumab and platinum-doublet chemotherapy or platinum-doublet chemotherapy, respectively (Figure 9).

Figure 9: Overall Survival - CHECKMATE-9LA

Second-line Treatment of Metastatic Squamous NSCLC

CHECKMATE-017 (NCT01642004) was a randomized (1:1), open-label trial in 272 patients with metastatic squamous NSCLC who had experienced disease progression during or after one prior platinum doublet-based chemotherapy regimen. Patients received OPDIVO 3 mg/kg by intravenous infusion every 2 weeks (n=135) or docetaxel 75 mg/m^2 intravenously every 3 weeks (n=137). Randomization was stratified by prior paclitaxel vs. other prior treatment and region (US/Canada vs. Europe vs. Rest of World). This trial included patients regardless of their PD-L1 status. The trial excluded patients with autoimmune disease, medical conditions requiring systemic immunosuppression, symptomatic interstitial lung disease, or untreated brain metastasis. Patients with treated brain metastases were eligible if neurologically returned to baseline at least 2 weeks prior to enrollment, and either off corticosteroids, or on a stable or decreasing dose of <10 mg daily prednisone equivalents. The first tumor assessments were conducted 9 weeks after randomization and continued every 6 weeks thereafter. The major efficacy outcome measure was OS. Additional efficacy outcome measures were investigator-assessed ORR and PFS.

The trial population characteristics were: median age was 63 years (range: 39 to 85) with 44% ≥65 years of age and 11% ≥75 years of age. The majority of patients were White (93%) and male (76%); the majority of patients were enrolled in Europe (57%) with the remainder in US/Canada (32%) and the rest of the world (11%). Baseline ECOG performance status was 0 (24%) or 1 (76%) and 92% were former/current smokers. Baseline disease characteristics of the population as reported by investigators were Stage IIIb (19%), Stage IV (80%), and brain metastases (6%). All patients received prior therapy with a platinum-doublet regimen and 99% of patients had tumors of squamous-cell histology.

The trial demonstrated a statistically significant improvement in OS for patients randomized to OPDIVO as compared with docetaxel at the prespecified interim analysis when 199 events were observed (86% of the planned number of events for final analysis). Efficacy results are shown in Table 64 and Figure 10.

Table 64: Efficacy Results - CHECKMATE-017
 | OPDIVO (n=135) | Docetaxel (n=137)
Overall Survival
Deaths (%) | 86 (64%) | 113 (82%)
Median (months) (95% CI) | 9.2 (7.3, 13.3) | 6.0 (5.1, 7.3)
Hazard ratio (95% CI)a | 0.59 (0.44, 0.79)
p-valueb,c | 0.0002
Overall Response Rate | 27 (20%) | 12 (9%)
(95% CI) | (14, 28) | (5, 15)
p-valued | 0.0083
Complete response | 1 (0.7%) | 0
Median duration of response (months) (95% CI) | NRe (9.8, NRe) | 8.4 (3.6, 10.8)
Progression-free Survival
Disease progression or death (%) | 105 (78%) | 122 (89%)
Median (months) | 3.5 | 2.8
Hazard ratio (95% CI)a | 0.62 (0.47, 0.81)
p-valueb | 0.0004
a Based on a stratified proportional hazards model.
b Based on stratified log-rank test.
c p-value is compared with 0.0315 of the allocated alpha for this interim analysis.
d Based on the stratified Cochran-Mantel-Haenszel test.
e Not Reached.

Figure 10: Overall Survival - CHECKMATE-017

Archival tumor specimens were retrospectively evaluated for PD-L1 expression. Across the trial population, 17% of 272 patients had non-quantifiable results. Among the 225 patients with quantifiable results, 47% had PD-L1 negative squamous NSCLC, defined as <1% of tumor cells expressing PD-L1 and 53% had PD-L1 positive squamous NSCLC defined as ≥1% of tumor cells expressing PD-L1. In pre-specified exploratory subgroup analyses, the hazard ratios for survival were 0.58 (95% CI: 0.37, 0.92) in the PD-L1 negative subgroup and 0.69 (95% CI: 0.45, 1.05) in the PD-L1 positive subgroup.

Second-line Treatment of Metastatic Non-Squamous NSCLC

CHECKMATE-057 (NCT01673867) was a randomized (1:1), open-label trial in 582 patients with metastatic non-squamous NSCLC who had experienced disease progression during or after one prior platinum doublet-based chemotherapy regimen. Appropriate prior targeted therapy in patients with known sensitizing EGFR mutation or ALK translocation was allowed. Patients received OPDIVO 3 mg/kg by intravenous infusion every 2 weeks (n=292) or docetaxel 75 mg/m^2 intravenously every 3 weeks (n=290). Randomization was stratified by prior maintenance therapy (yes vs. no) and number of prior therapies (1 vs. 2). The trial excluded patients with autoimmune disease, medical conditions requiring systemic immunosuppression, symptomatic interstitial lung disease, or untreated brain metastasis. Patients with treated brain metastases were eligible if neurologically stable. The first tumor assessments were conducted 9 weeks after randomization and continued every 6 weeks thereafter. The major efficacy outcome measure was OS. Additional efficacy outcome measures were investigator-assessed ORR and PFS. In addition, prespecified analyses were conducted in subgroups defined by PD-L1 expression.

The trial population characteristics: median age was 62 years (range: 21 to 85) with 42% of patients ≥65 years and 7% of patients ≥75 years. The majority of patients were White (92%) and male (55%); the majority of patients were enrolled in Europe (46%) followed by the US/Canada (37%) and the rest of the world (17%). Baseline ECOG performance status was 0 (31%) or 1 (69%), 79% were former/current smokers, 3.6% had NSCLC with ALK rearrangement, 14% had NSCLC with EGFR mutation, and 12% had previously treated brain metastases. Prior therapy included platinum-doublet regimen (100%) and 40% received maintenance therapy as part of the first-line regimen. Histologic subtypes included adenocarcinoma (93%), large cell (2.4%), and bronchoalveolar (0.9%).

CHECKMATE-057 demonstrated a statistically significant improvement in OS for patients randomized to OPDIVO as compared with docetaxel at the prespecified interim analysis when 413 events were observed (93% of the planned number of events for final analysis). Efficacy results are shown in Table 65 and Figure 11.

Table 65: Efficacy Results - CHECKMATE-057
 | OPDIVO (n=292) | Docetaxel (n=290)
Overall Survival
Deaths (%) | 190 (65%) | 223 (77%)
Median (months) (95% CI) | 12.2 (9.7, 15.0) | 9.4 (8.0, 10.7)
Hazard ratio (95% CI)a | 0.73 (0.60, 0.89)
p-valueb,c | 0.0015
Overall Response Rate | 56 (19%) | 36 (12%)
(95% CI) | (15, 24) | (9, 17)
p-valued | 0.02
Complete response | 4 (1.4%) | 1 (0.3%)
Median duration of response (months) (95% CI) | 17 (8.4, NRe) | 6 (4.4, 7.0)
Progression-free Survival
Disease progression or death (%) | 234 (80%) | 245 (84%)
Median (months) | 2.3 | 4.2
Hazard ratio (95% CI)a | 0.92 (0.77, 1.11)
p-valueb | 0.39
a Based on a stratified proportional hazards model.
b Based on stratified log-rank test.
c p-value is compared with .0408 of the allocated alpha for this interim analysis.
d Based on the stratified Cochran-Mantel-Haenszel test.
e Not Reached.

Figure 11: Overall Survival - CHECKMATE-057

Archival tumor specimens were evaluated for PD-L1 expression following completion of the trial. Across the trial population, 22% of 582 patients had non-quantifiable results. Of the remaining 455 patients, the proportion of patients in retrospectively determined subgroups based on PD-L1 testing using the PD-L1 IHC 28-8 pharmDx assay were: 46% PD-L1 negative, defined as <1% of tumor cells expressing PD-L1 and 54% had PD-L1 expression, defined as ≥1% of tumor cells expressing PD-L1. Among the 246 patients with tumors expressing PD-L1, 26% had ≥1% but <5% tumor cells with positive staining, 7% had ≥5% but <10% tumor cells with positive staining, and 67% had ≥10% tumor cells with positive staining. Figures 12 and 13 summarize the results of prespecified analyses of OS and PFS in subgroups determined by percentage of tumor cells expressing PD-L1.

Figure 12: Forest Plot: OS Based on PD-L1 Expression - CHECKMATE-057

Figure 13: Forest Plot: PFS Based on PD-L1 Expression - CHECKMATE-057

14.6 Malignant Pleural Mesothelioma

CHECKMATE-743 (NCT02899299) was a randomized, open-label trial in patients with unresectable malignant pleural mesothelioma. The trial included patients with histologically confirmed and previously untreated malignant pleural mesothelioma with no palliative radiotherapy within 14 days of initiation of therapy. Patients with interstitial lung disease, active autoimmune disease, medical conditions requiring systemic immunosuppression, or active brain metastasis were excluded from the trial.

Patients were randomized 1:1 to receive either:

- OPDIVO 3 mg/kg over 30 minutes by intravenous infusion every 2 weeks and ipilimumab 1 mg/kg over 30 minutes by intravenous infusion every 6 weeks for up to 2 years, or
- cisplatin 75 mg/m^2 and pemetrexed 500 mg/m^2, or carboplatin 5 AUC and pemetrexed 500 mg/m^2 administered every 3 weeks for 6 cycles.

Stratification factors for randomization were tumor histology (epithelioid vs. sarcomatoid or mixed histology subtypes) and sex (male vs. female). Study treatment continued for up to 2 years, or until disease progression or unacceptable toxicity. Patients who discontinued combination therapy because of an adverse reaction attributed to ipilimumab were permitted to continue OPDIVO as a single agent. Treatment could continue beyond disease progression if a patient was clinically stable and was considered to be deriving clinical benefit by the investigator. Tumor assessments were performed every 6 weeks from the first dose of study treatment for the first 12 months, then every 12 weeks until disease progression or study treatment was discontinued. The primary efficacy outcome measure was OS. Additional efficacy outcome measures included PFS, ORR, and duration of response as assessed by BICR utilizing modified RECIST criteria.

A total of 605 patients were randomized to receive either OPDIVO in combination with ipilimumab (n=303) or chemotherapy (n=302). The median age was 69 years (range: 25 to 89), with 72% of patients ≥65 years and 26% ≥75 years; 85% were White, 11% were Asian, and 77% were male. Baseline ECOG performance status was 0 (40%) or 1 (60%), 35% had Stage III and 51% had Stage IV disease, 75% had epithelioid and 25% had non-epithelioid histology, 75% had tumors with PD-L1 expression ≥1%, and 22% had tumors with PD-L1 expression <1%.

The trial demonstrated a statistically significant improvement in OS for patients randomized to OPDIVO in combination with ipilimumab compared to chemotherapy. Efficacy results from the prespecified interim analysis are presented in Table 66 and Figure 14.

Table 66: Efficacy Results - CHECKMATE-743
 | OPDIVO and Ipilimumab (n=303) | Chemotherapy (n=302)
Overall Survivala
Events (%) | 200 (66) | 219 (73)
Median (months)b; (95% CI) | 18.1 (16.8, 21.5) | 14.1 (12.5, 16.2)
Hazard ratio (95% CI)c | 0.74 (0.61, 0.89)
Stratified log-rank p-valued | 0.002
Progression-free Survival
Events (%) | 218 (72) | 209 (69)
Hazard ratio (95% CI)c | 1.0 (0.82, 1.21)
Median (months)b; (95% CI) | 6.8 (5.6, 7.4) | 7.2 (6.9, 8.1)
Overall Response Ratee | 40% | 43%
(95% CI) | (34, 45) | (37, 49)
Duration of Response
Median (months)b (95% CI) | 11.0 (8.1, 16.5) | 6.7 (5.3, 7.1)
a At the time of the interim analysis, 419 deaths (89% of the deaths needed for the final analysis) had occurred.
b Kaplan-Meier estimate.
c Stratified Cox proportional hazard model.
d p-value is compared with the allocated alpha of 0.0345 for this interim analysis.
e Based on confirmed response by BICR.

Figure 14: Overall Survival - CHECKMATE-743

In a prespecified exploratory analysis based on histology, in the subgroup of patients with epithelioid histology, the hazard ratio (HR) for OS was 0.85 (95% CI: 0.68, 1.06), with median OS of 18.7 months in the OPDIVO and ipilimumab arm and 16.2 months in the chemotherapy arm. In the subgroup of patients with non-epithelioid histology, the HR for OS was 0.46 (95% CI: 0.31, 0.70), with median OS of 16.9 months in the OPDIVO and ipilimumab arm and 8.8 months in the chemotherapy arm.

14.7 Advanced Renal Cell Carcinoma

First-line Renal Cell Carcinoma

CHECKMATE-214

CHECKMATE-214 (NCT02231749) was a randomized (1:1), open-label trial in patients with previously untreated advanced RCC. Patients were included regardless of their PD-L1 status. CHECKMATE-214 excluded patients with any history of or concurrent brain metastases, active autoimmune disease, or medical conditions requiring systemic immunosuppression. Patients were stratified by International Metastatic RCC Database Consortium (IMDC) prognostic score and region.

Efficacy was evaluated in intermediate/poor risk patients with at least 1 or more of 6 prognostic risk factors as per the IMDC criteria (less than one year from time of initial renal cell carcinoma diagnosis to randomization, Karnofsky performance status <80%, hemoglobin less than the lower limit of normal, corrected calcium of >10 mg/dL, platelet count greater than the upper limit of normal, and absolute neutrophil count greater than the upper limit of normal).

Patients were randomized to OPDIVO 3 mg/kg and ipilimumab 1 mg/kg intravenously every 3 weeks for 4 doses followed by OPDIVO 3 mg/kg intravenously every two weeks (n=425), or sunitinib 50 mg orally daily for the first 4 weeks of a 6-week cycle (n=422). Treatment continued until disease progression or unacceptable toxicity.

The trial population characteristics were: median age was 61 years (range: 21 to 85) with 38% ≥65 years of age and 8% ≥75 years of age. The majority of patients were male (73%) and White (87%) and 26% and 74% of patients had a baseline KPS of 70% to 80% and 90% to 100%, respectively.

The major efficacy outcome measures were OS, PFS (independent radiographic review committee [IRRC]-assessed) and confirmed ORR (IRRC-assessed) in intermediate/poor risk patients. In this population, the trial demonstrated statistically significant improvement in OS and ORR for patients randomized to OPDIVO and ipilimumab as compared with sunitinib (Table 67 and Figure 15). OS benefit was observed regardless of PD-L1 expression level. The trial did not demonstrate a statistically significant improvement in PFS. Efficacy results are shown in Table 67 and Figure 15.

Table 67: Efficacy Results - CHECKMATE-214
 | Intermediate/Poor-Risk
 | OPDIVO and Ipilimumab (n=425) | Sunitinib (n=422)
Overall Survival
Deaths (%) | 140 (32.9) | 188 (44.5)
Median survival (months) | NRa | 25.9
Hazard ratio (99.8% CI)b | 0.63 (0.44, 0.89)
p-valuec,d | <0.0001
Confirmed Overall Response Rate (95% CI) | 41.6% (36.9, 46.5) | 26.5% (22.4, 31.0)
p-valuee,f | <0.0001
Complete response (CR) | 40 (9.4) | 5 (1.2)
Partial response (PR) | 137 (32.2) | 107 (25.4)
Median duration of response (months) (95% CI) | NRa (21.8, NRa) | 18.2 (14.8, NRa)
Progression-free Survival
Disease progression or death (%) | 228 (53.6) | 228 (54.0)
Median (months) | 11.6 | 8.4
Hazard ratio (99.1% CI)a | 0.82 (0.64, 1.05)
p-valuec | NSg
a Not Reached.
b Based on a stratified proportional hazards model.
c Based on a stratified log-rank test.
d p-value is compared to alpha 0.002 in order to achieve statistical significance.
e Based on the stratified DerSimonian-Laird test.
f p-value is compared to alpha 0.001 in order to achieve statistical significance.
g Not Significant at alpha level of 0.009.

Figure 15: Overall Survival (Intermediate/Poor Risk Population) - CHECKMATE-214

CHECKMATE-214 also randomized 249 favorable risk patients as per IMDC criteria to OPDIVO and ipilimumab (n=125) or to sunitinib (n=124). These patients were not evaluated as part of the efficacy analysis population. OS in favorable risk patients receiving OPDIVO and ipilimumab compared to sunitinib has a hazard ratio of 1.45 (95% CI: 0.75, 2.81). The efficacy of OPDIVO and ipilimumab in previously untreated renal cell carcinoma with favorable-risk disease has not been established.

CHECKMATE-9ER

CHECKMATE-9ER (NCT03141177) was a randomized, open-label study of OPDIVO combined with cabozantinib versus sunitinib in patients with previously untreated advanced RCC. CHECKMATE-9ER excluded patients with autoimmune disease or other medical conditions requiring systemic immunosuppression. Patients were stratified by IMDC prognostic score (favorable vs. intermediate vs. poor), PD-L1 tumor expression (≥1% vs. <1% or indeterminate), and region (US/Canada/Western Europe/Northern Europe vs. Rest of World).

Patients were randomized to OPDIVO 240 mg intravenously every 2 weeks and cabozantinib 40 mg orally daily (n=323), or sunitinib 50 mg orally daily for the first 4 weeks of a 6-week cycle (4 weeks on treatment followed by 2 weeks off) (n=328). Treatment continued until disease progression per RECIST v1.1 or unacceptable toxicity. Treatment beyond RECIST-defined disease progression was permitted if the patient was clinically stable and considered to be deriving clinical benefit by the investigator. Tumor assessments were performed at baseline, after randomization at Week 12, then every 6 weeks until Week 60, and then every 12 weeks thereafter.

The trial population characteristics were: median age 61 years (range: 28 to 90) with 38% ≥65 years of age and 10% ≥75 years of age. The majority of patients were male (74%) and White (82%) and 23% and 77% of patients had a baseline KPS of 70% to 80% and 90% to 100%, respectively. Patient distribution by IMDC risk categories was 22% favorable, 58% intermediate, and 20% poor.

The major efficacy outcome measure was PFS (BICR assessed). Additional efficacy outcome measures were OS and ORR (BICR assessed). The trial demonstrated a statistically significant improvement in PFS, OS, and ORR for patients randomized to OPDIVO and cabozantinib compared with sunitinib. Consistent results for PFS were observed across pre-specified subgroups of IMDC risk categories and PD-L1 tumor expression status. An updated OS analysis was conducted when 271 deaths were observed based on the pre-specified number of deaths for the pre-planned final analysis of OS. Efficacy results are shown in Table 68 and Figures 16 and 17.

Table 68: Efficacy Results - CHECKMATE-9ER
 | OPDIVO and Cabozantinib (n=323) | Sunitinib (n=328)
Progression-free Survival
Disease progression or death (%) | 144 (45) | 191 (58)
Median PFS (months)a (95% CI) | 16.6 (12.5, 24.9) | 8.3 (7.0, 9.7)
Hazard ratio (95% CI)b | 0.51 (0.41, 0.64)
p-valuec,d | <0.0001
Overall Survival
Deaths (%) | 67 (21) | 99 (30)
Median OS (months)a (95% CI) | NRe | NR (22.6, NRe)
Hazard ratio (98.89% CI)b | 0.60 (0.40, 0.89)
p-valuec,d,f | 0.0010
Updated Overall Survival
Deaths (%) | 121 (37) | 150 (46)
Median OS (months)a (95% CI) | 37.7 (35.5, NR) | 34.3 (29.0, NR)
Hazard ratio (95% CI)b | 0.70 (0.55, 0.90)
Confirmed Objective Response Rate (95% CI)g | 55.7% (50.1, 61.2) | 27.1% (22.4, 32.3)
p-valueh | <0.0001
Complete Response | 26 (8%) | 15 (4.6%)
Partial Response | 154 (48%) | 74 (23%)
Median duration of response in months (95% CI)a | 20.2 (17.3, NRe) | 11.5 (8.3, 18.4)
a Based on Kaplan-Meier estimates.
b Stratified Cox proportional hazards model.
c Based on stratified log-rank test.
d 2-sided p-values from stratified log-rank test.
e Not Reached.
f p-value is compared with the allocated alpha of 0.0111 for this interim analysis.
g CI based on the Clopper-Pearson method.
h 2-sided p-value from Cochran-Mantel-Haenszel test.

Figure 16: Progression-free Survival - CHECKMATE-9ER

Figure 17: Updated Overall Survival - CHECKMATE-9ER

In an exploratory analysis, the updated analysis of OS in patients with IMDC favorable, intermediate, intermediate/poor, and poor risk demonstrated a HR (95% CI) of 1.03 (0.55, 1.92), 0.74 (0.54, 1.01), 0.65 (0.50, 0.85), and 0.49 (0.31, 0.79), respectively.

Previously Treated Renal Cell Carcinoma

CHECKMATE-025

CHECKMATE-025 (NCT01668784) was a randomized (1:1), open-label trial in patients with advanced RCC who had experienced disease progression during or after one or two prior anti-angiogenic therapy regimens. Patients had to have a Karnofsky Performance Score (KPS) ≥70% and patients were included regardless of their PD-L1 status. The trial excluded patients with any history of or concurrent brain metastases, prior treatment with an mTOR inhibitor, active autoimmune disease, or medical conditions requiring systemic immunosuppression. Patients were stratified by region, Memorial Sloan Kettering Cancer Center (MSKCC) Risk Group and the number of prior anti-angiogenic therapies. Patients were randomized OPDIVO 3 mg/kg by intravenous infusion every 2 weeks (n=410) or everolimus 10 mg orally daily (n=411). The first tumor assessments were conducted 8 weeks after randomization and continued every 8 weeks thereafter for the first year and then every 12 weeks until progression or treatment discontinuation, whichever occurred later. The major efficacy outcome measure was overall survival (OS).

The trial population characteristics were: median age was 62 years (range: 18 to 88) with 40% ≥65 years of age and 9% ≥75 years of age. The majority of patients were male (75%) and White (88%) and 34% and 66% of patients had a baseline KPS of 70% to 80% and 90% to 100%, respectively. The majority of patients (77%) were treated with one prior anti-angiogenic therapy. Patient distribution by MSKCC risk groups was 34% favorable, 47% intermediate, and 19% poor.

The trial demonstrated a statistically significant improvement in OS for patients randomized to OPDIVO as compared with everolimus at the prespecified interim analysis when 398 events were observed (70% of the planned number of events for final analysis). OS benefit was observed regardless of PD-L1 expression level. Efficacy results are shown in Table 69 and Figure 18.

Table 69: Efficacy Results - CHECKMATE-025
 | OPDIVO (n=410) | Everolimus (n=411)
Overall Survival
Deaths (%) | 183 (45) | 215 (52)
Median survival (months) (95% CI) | 25.0 (21.7, NRa) | 19.6 (17.6, 23.1)
Hazard ratio (95% CI)b | 0.73 (0.60, 0.89)
p-valuec,d | 0.0018
Confirmed Overall Response Rate (95% CI) | 21.5% (17.6, 25.8) | 3.9% (2.2, 6.2)
Median duration of response (months) (95% CI) | 23.0 (12.0, NRa) | 13.7 (8.3, 21.9)
Median time to onset of confirmed response (months) (min, max) | 3.0 (1.4, 13.0) | 3.7 (1.5, 11.2)
a Not Reached.
b Based on a stratified proportional hazards model.
c Based on a stratified log-rank test.
d p-value is compared with 0.0148 of the allocated alpha for this interim analysis.

Figure 18: Overall Survival - CHECKMATE-025

14.8 Classical Hodgkin Lymphoma

Two studies evaluated the efficacy of OPDIVO as a single agent in adult patients with cHL after failure of autologous HSCT.

CHECKMATE-205 (NCT02181738) was a single-arm, open-label, multicenter, multicohort trial in cHL. CHECKMATE-039 (NCT01592370) was an open-label, multicenter, dose escalation trial that included cHL. Both studies included patients regardless of their tumor PD-L1 status and excluded patients with ECOG performance status of 2 or greater, autoimmune disease, symptomatic interstitial lung disease, hepatic transaminases more than 3 times ULN, creatinine clearance <40 mL/min, prior allogeneic HSCT, or chest irradiation within 24 weeks. In addition, both studies required an adjusted diffusion capacity of the lungs for carbon monoxide (DLCO) of over 60% in patients with prior pulmonary toxicity.

Patients received OPDIVO 3 mg/kg by intravenous infusion every 2 weeks until disease progression, maximal clinical benefit, or unacceptable toxicity. A cycle consisted of one dose. Dose reduction was not permitted.

Efficacy was evaluated by ORR as determined by an IRRC. Additional outcome measures included duration of response (DOR).

Efficacy was evaluated in 95 patients in CHECKMATE-205 and CHECKMATE-039 combined who had failure of autologous HSCT and post-transplantation brentuximab vedotin. The median age was 37 years (range: 18 to 72). The majority were male (64%) and White (87%). Patients had received a median of 5 prior systemic regimens (range: 2 to 15). They received a median of 27 doses of OPDIVO (range: 3 to 48), with a median duration of therapy of 14 months (range: 1 to 23 months). Efficacy results are shown in Table 70.

Table 70: Efficacy in cHL after Autologous HSCT and Post-transplantation Brentuximab Vedotin
 | CHECKMATE-205 and CHECKMATE-039 (n=95)
Overall Response Rate, n (%)a (95% CI) | 63 (66%) (56, 76)
Complete remission rate (95% CI) | 6 (6%) (2, 13)
Partial remission rate (95% CI) | 57 (60%) (49, 70)
Duration of Response (months) Medianb (95% CI) Rangec | 13.1 (9.5, NRd) 0+, 23.1+
Time to Response (months) Median Range | 2.0 0.7, 11.1
a Per 2007 revised International Working Group criteria.
b Kaplan-Meier estimate. Among responders, the median follow-up for DOR, measured from the date of first response, was 9.9 months.
c A + sign indicates a censored value.
d Not Reached.

Efficacy was also evaluated in 258 patients in CHECKMATE-205 and CHECKMATE-039 combined who had relapsed or progressive cHL after autologous HSCT. The analysis included the group described above. The median age was 34 years (range: 18 to 72). The majority were male (59%) and White (86%). Patients had a median of 4 prior systemic regimens (range: 2 to 15), with 85% having 3 or more prior systemic regimens and 76% having prior brentuximab vedotin. Of the 195 patients having prior brentuximab vedotin, 17% received it only before autologous HSCT, 78% received it only after HSCT, and 5% received it both before and after HSCT. Patients received a median of 21 doses of OPDIVO (range: 1 to 48), with a median duration of therapy of 10 months (range: 0 to 23 months). Efficacy results are shown in Table 71.

Table 71: Efficacy in cHL after Autologous HSCT
 | CHECKMATE-205 and CHECKMATE-039 (n=258)
Overall Response Rate, n (%) (95% CI) | 179 (69%) (63, 75)
Complete remission rate (95% CI) | 37 (14%) (10, 19)
Partial remission rate (95% CI) | 142 (55%) (49, 61)
Duration of Response (months) Mediana, b (95% CI) Range | NRc (12.0, NRc) 0+, 23.1+
Time to Response (months) Median Range | 2.0 0.7, 11.1
a Kaplan-Meier estimate. Among responders, the median follow-up for DOR, measured from the date of first response, was 6.7 months.
b The estimated median duration of PR was 13.1 months (95% CI, 9.5, NE). The median duration of CR was not reached.
c Not Reached.

14.9 Recurrent or Metastatic Squamous Cell Carcinoma of the Head and Neck

CHECKMATE-141 (NCT02105636) was a randomized (2:1), active-controlled, open-label trial enrolling patients with metastatic or recurrent SCCHN who had experienced disease progression during or within 6 months of receiving platinum-based therapy administered in either the adjuvant, neo-adjuvant, primary (unresectable locally advanced) or metastatic setting. The trial excluded patients with autoimmune disease, medical conditions requiring immunosuppression, recurrent or metastatic carcinoma of the nasopharynx, squamous cell carcinoma of unknown primary histology, salivary gland or non-squamous histologies (e.g., mucosal melanoma), or untreated brain metastasis. Patients with treated brain metastases were eligible if neurologically stable. Patients were randomized to receive OPDIVO 3 mg/kg by intravenous infusion every 2 weeks or investigator’s choice of cetuximab (400 mg/m^2 initial dose intravenously followed by 250 mg/m^2 weekly), or methotrexate (40 to 60 mg/m^2 intravenously weekly), or docetaxel (30 to 40 mg/m^2 intravenously weekly).

Randomization was stratified by prior cetuximab treatment (yes/no). The first tumor assessments were conducted 9 weeks after randomization and continued every 6 weeks thereafter. The major efficacy outcome measure was OS. Additional efficacy outcome measures were PFS and ORR.

A total of 361 patients were randomized; 240 patients to the OPDIVO arm and 121 patients to the investigator’s choice arm (docetaxel: 45%; methotrexate: 43%; and cetuximab: 12%). The trial population characteristics were: median age was 60 years (range: 28 to 83) with 31% ≥65 years of age, 83% were White, 12% Asian, and 4% were Black, and 83% male. Baseline ECOG performance status was 0 (20%) or 1 (78%), 76% were former/current smokers, 90% had Stage IV disease, 45% of patients received only one prior line of systemic therapy, the remaining 55% received two or more prior lines of systemic therapy, and 25% had HPVp16-positive tumors, 24% had HPV p16-negative tumors, and 51% had unknown status.

The trial demonstrated a statistically significant improvement in OS for patients randomized to OPDIVO as compared with investigator’s choice at a pre-specified interim analysis (78% of the planned number of events for final analysis). There were no statistically significant differences between the two arms for PFS (HR=0.89; 95% CI: 0.70, 1.13) or ORR (13.3% [95% CI: 9.3, 18.3] vs. 5.8% [95% CI: 2.4, 11.6] for nivolumab and investigator’s choice, respectively). Efficacy results are shown in Table 72 and Figure 19.

Table 72: Overall Survival - CHECKMATE-141
 | OPDIVO (n=240) | Cetuximab, Methotrexate or Docetaxel (n=121)
Overall Survival
Deaths (%) | 133 (55%) | 85 (70%)
Median (months) (95% CI) | 7.5 (5.5, 9.1) | 5.1 (4.0, 6.0)
Hazard ratio (95% CI)a | 0.70 (0.53, 0.92)
p-valueb,c | 0.0101
a Based on stratified proportional hazards model.
b Based on stratified log-rank test.
c p-value is compared with 0.0227 of the allocated alpha for this interim analysis.

Figure 19: Overall Survival - CHECKMATE-141

Archival tumor specimens were retrospectively evaluated for PD-L1 expression using the PD-L1 IHC 28-8 pharmDx assay. Across the trial population, 28% (101/361) of patients had non-quantifiable results. Among the 260 patients with quantifiable results, 43% (111/260) had PD-L1 negative SCCHN, defined as <1% of tumor cells expressing PD-L1, and 57% (149/260) had PD-L1 positive SCCHN, defined as ≥1% of tumor cells expressing PD-L1. In pre-specified exploratory subgroup analyses, the hazard ratio for survival was 0.89 (95% CI: 0.54, 1.45) with median survivals of 5.7 and 5.8 months for the nivolumab and chemotherapy arms, respectively, in the PD-L1 negative subgroup. The HR for survival was 0.55 (95% CI: 0.36, 0.83) with median survivals of 8.7 and 4.6 months for the nivolumab and chemotherapy arms, respectively, in the PD-L1 positive SCCHN subgroup.

14.10 Urothelial Carcinoma

Adjuvant Treatment of UC at High Risk of Recurrence

CHECKMATE-274 (NCT02632409) was a randomized, double-blind, placebo-controlled study of adjuvant OPDIVO in patients who were within 120 days of radical resection (R0) of UC of the bladder or upper urinary tract (renal pelvis or ureter) at high risk of recurrence. High risk of recurrence was defined as either 1) ypT2-ypT4a or ypN^+ for patients who received neoadjuvant cisplatin or 2) pT3-pT4a or pN^+ for patients who did not receive neoadjuvant cisplatin and who also either were ineligible for or refused adjuvant cisplatin. Patients were randomized 1:1 to receive OPDIVO 240 mg or placebo by intravenous infusion every 2 weeks until recurrence or until unacceptable toxicity for a maximum treatment duration of 1 year. Patients were stratified by pathologic nodal status (N+ vs. N0/x with <10 nodes removed vs. N0 with ≥10 nodes removed), tumor cells expressing PD-L1 (≥1% vs. <1%/indeterminate as determined by the central lab using the PD-L1 IHC 28-8 pharmDx assay), and use of neoadjuvant cisplatin (yes vs. no).

The trial population characteristics were: median age of 67 years (range: 30 to 92); 76% male; 76% White, 22% Asian, 0.7% Black, and 0.1% American Indian or Alaska Native. Of the 335 (47%) of patients with node-positive UC, 44 (6%) had non–muscle-invasive (<pT2) primary tumors. ECOG performance status was 0 (63%), 1 (35%), or 2 (2%). Prior neoadjuvant cisplatin had been given to 43% of patients; of the 57% who did not receive prior neoadjuvant cisplatin, reasons listed were ineligibility (22%), patient preference (33%), and other/not reported (2%). Tumor PD-L1 expression was ≥1% in 40% of patients, and 21% of patients had upper tract UC.

The major efficacy outcome measures were investigator-assessed DFS in all randomized patients and in patients with tumors expressing PD-L1 ≥1%. DFS was defined as time to first recurrence (local urothelial tract, local non-urothelial tract, or distant metastasis), or death. Additional efficacy outcome measures included OS.

At the pre-specified interim analysis, CHECKMATE-274 demonstrated a statistically significant improvement in DFS for patients randomized to OPDIVO vs. placebo in the all randomized patient population, as well as in the subpopulation of patients with PD-L1 ≥1%, as shown in Table 73 and Figure 20.

In exploratory subgroup analyses in patients with upper tract UC (n=149), no improvement in DFS was observed in the nivolumab arm compared to the placebo arm. The unstratified DFS hazard ratio estimate was 1.15 (95% CI: 0.74, 1.80).

In an exploratory subgroup analysis in patients with PD-L1 expression of <1% (n=414), the unstratified DFS hazard ratio estimate was 0.83 (95% CI: 0.64, 1.08).

OS data is immature with 33% of deaths in the overall randomized population. In the UTUC subpopulation, 37 deaths occurred (20 in the nivolumab arm, 17 in the placebo arm).

Table 73: Efficacy Results - CHECKMATE-274
 | All Randomized |  | PD-L1 ≥1%
 | OPDIVO (n=353) | Placebo (n=356) | OPDIVO (n=140) | Placebo (n=142)
Disease-free Survival
Eventsa, n (%) Local recurrence Distant recurrence Death | 170 (48) 47 (13) 108 (31) 14 (4) | 204 (57) 64 (18) 127 (36) 10 (3) | 55 (39) 10 (7) 40 (29) 5 (4) | 81 (57) 24 (17) 52 (37) 5 (4)
Median DFS (months)b (95% CI) | 20.8 (16.5, 27.6) | 10.8 (8.3, 13.9) | N.R. (21.2, N.E.) | 8.4 (5.6, 21.2)
Hazard ratioc (95% CI) | 0.70 (0.57, 0.86) |  | 0.55 (0.39, 0.77)
p-value | 0.0008d |  | 0.0005e
N.R. Not Reached, N.E. Not Estimable
a Includes disease at baseline events (protocol deviations): n=1 in OPDIVO arm and n=3 in placebo arm.
b Based on Kaplan-Meier estimates.
c Stratified Cox proportional hazard model. Hazard ratio is OPDIVO over placebo.
d Log-rank test stratified by prior neoadjuvant cisplatin, pathological nodal status, PD-L1 status (≥1% vs <1%/indeterminate). Boundary for statistical significance in all randomized patients: p-value <0.01784.
e Log-rank test stratified by prior neoadjuvant cisplatin, pathological nodal status. Boundary for statistical significance in all randomized patients with PD-L1 ≥1%: p-value <0.01282.

Figure 20: Disease-free Survival in All Randomized Patients - CHECKMATE-274

First-line Treatment of Unresectable or Metastatic UC

CHECKMATE-901 (NCT 03036098) was a randomized, open-label study in patients with previously untreated unresectable or metastatic UC. Prior neoadjuvant or adjuvant chemotherapy were permitted as long as the disease recurrence took place ≥12 months from completion of therapy. Patients who were ineligible for cisplatin and those with active CNS metastases were excluded. Stratification factors for randomization were PD-L1 status (≥1% vs. <1% or indeterminate) and liver metastasis. Patients were randomized 1:1 to receive either:

- OPDIVO 360 mg and cisplatin 70 mg/m^2 on Day 1 and gemcitabine 1000 mg/m^2 on Days 1 and 8 of a 21-day cycle of a 21-day cycle for up to 6 cycles followed by single-agent OPDIVO 480 mg every 4 weeks until disease progression or unacceptable toxicity. In the absence of disease progression or unacceptable toxicity, OPDIVO was continued for up to 2 years from first dose.
- Cisplatin 70 mg/m^2 on Day 1 and gemcitabine 1000 mg/m^2 on Days 1 and 8 of a 21-day cycle for up to 6 cycles, until disease progression or unacceptable toxicity.

The major efficacy outcome measures were OS and PFS as assessed by BICR using RECIST v1.1. Additional efficacy outcome measures included ORR as assessed by BICR.

The median age was 65 years of age (range: 32 to 86) with 51% of patients ≥65 years of age and 12% of patients ≥75 years of age, 23% were Asian, 72% were White, 0.3% were Black, 0.3% were American Indian or Alaska Native, 4.9% were Other, 12% were Hispanic or Latino, and 77% were male. Baseline ECOG performance status was 0 (53%) or 1 (46%). At baseline, 87% of patients had metastatic UC, including 20% with liver metastases, 11% had locally advanced UC, and 51% had UC histologic variants. Forty-nine (16%) in the OPDIVO in combination with cisplatin-based chemotherapy arm and 43 (14%) in the cisplatin-based chemotherapy arm switched from cisplatin to carboplatin after at least one cycle of cisplatin.

Efficacy results are presented in Table 74 and Figures 21 and 22.

Table 74: Efficacy Results – CHECKMATE 901
 | OPDIVO and Cisplatin and Gemcitabine (n=304) | Cisplatin and Gemcitabine (n=304)
Overall Survival (OS)
Events, n (%) | 172 (56.6) | 193 (63.5)
Median (months) (95% CI)a | 21.7 (18.6, 26.4) | 18.9 (14.7, 22.4)
Hazard ratio (95% CI)b | 0.78 (0.63, 0.96)
p-valuec | 0.0171
Progression-free Survival (PFS)d
Events, n (%) | 211 (69.4) | 191 (62.8)
Median (months) (95% CI)a | 7.9 (7.6, 9.5) | 7.6 (6.0, 7.8)
Hazard ratio (95% CI)b | 0.72 (0.59, 0.88)
p-valuec | 0.0012
Objective Response Rate (ORR)d
Response rate, n (%); (95% CI) | 175 (57.6%); (51.8, 63.2) | 131 (43.1%); (37.5, 48.9)
Complete response rate, n (%) | 66 (22%) | 36 (12%)
Partial response rate, n (%) | 109 (36%) | 95 (31%)
Duration of Response (DoR)
Median (months) (95% CI)a | 9.5 (7.6, 15.1) | 7.3 (5.7, 8.9)
a Based on Kaplan-Meier Estimates.
b Stratified Cox proportional hazard model.
c 2 sided p values from stratified log-rank test.
d Assessed by BICR.

Figure 21: Overall Survival - CHECKMATE-901

Figure 22: Progression-free Survival - CHECKMATE-901

Previously Treated Advanced or Metastatic UC

CHECKMATE-275 (NCT02387996) was a single-arm trial in 270 patients with locally advanced or metastatic UC who had disease progression during or following platinum-containing chemotherapy or who had disease progression within 12 months of treatment with a platinum-containing neoadjuvant or adjuvant chemotherapy regimen. Patients were excluded for active brain or leptomeningeal metastases, active autoimmune disease, medical conditions requiring systemic immunosuppression, and ECOG performance status >1. Patients received OPDIVO 3 mg/kg by intravenous infusion every 2 weeks until unacceptable toxicity or either radiographic or clinical progression. Tumor response assessments were conducted every 8 weeks for the first 48 weeks and every 12 weeks thereafter. Major efficacy outcome measures included confirmed ORR as assessed by IRRC using RECIST v1.1 and DOR.

The median age was 66 years (range: 38 to 90), 78% were male, 86% were White. Twenty-seven percent had non-bladder urothelial carcinoma and 84% had visceral metastases. Thirty-four percent of patients had disease progression following prior platinum-containing neoadjuvant or adjuvant therapy. Twenty-nine percent of patients had received ≥2 prior systemic regimens in the metastatic setting. Thirty-six percent of patients received prior cisplatin only, 23% received prior carboplatin only, and 7% were treated with both cisplatin and carboplatin in the metastatic setting. Forty-six percent of patients had an ECOG performance status of 1. Eighteen percent of patients had a hemoglobin <10 g/dL, and twenty-eight percent of patients had liver metastases at baseline. Patients were included regardless of their PD-L1 status.

Tumor specimens were evaluated prospectively using the PD-L1 IHC 28-8 pharmDx assay at a central laboratory and the results were used to define subgroups for pre-specified analyses. Of the 270 patients, 46% were defined as having PD-L1 expression of ≥1% (defined as ≥1% of tumor cells expressing PD-L1). The remaining 54% of patients were classified as having PD-L1 expression of <1% (defined as <1% of tumor cells expressing PD-L1). Confirmed ORR in all patients and the two PD-L1 subgroups are shown in Table 75. Median time to response was 1.9 months (range: 1.6-7.2). In 77 patients who received prior systemic therapy only in the neoadjuvant or adjuvant setting, the ORR was 23.4% (95% CI: 14.5%, 34.4%).

Table 75: Efficacy Results - CHECKMATE-275
 | All Patients N=270 | PD-L1 <1% N=146 | PD-L1 ≥1% N=124
Confirmed Overall Response Rate, n (%) (95% CI) | 53 (19.6%) (15.1, 24.9) | 22 (15.1%) (9.7, 21.9) | 31 (25.0%) (17.7, 33.6)
Complete response rate | 7 (2.6%) | 1 (0.7%) | 6 (4.8%)
Partial response rate | 46 (17.0%) | 21 (14.4%) | 25 (20.2%)
Median Duration of Responsea (months) (range) | 10.3 (1.9+, 12.0+) | 7.6 (3.7, 12.0+) | NRb (1.9+, 12.0+)
a Estimated from the Kaplan-Meier Curve.
b Not Reached.

14.11 Microsatellite Instability-High or Mismatch Repair Deficient Metastatic Colorectal Cancer

Treatment of MSI-H or dMMR mCRC In Combination with Ipilimumab

CHECKMATE-8HW (NCT03143153) was a randomized, 3-arm, open-label trial in immunotherapy-naive patients across all lines of therapy with unresectable or metastatic CRC with known tumor MSI-H or dMMR (MSI-H/dMMR) status as determined in accordance with local standard of practice using PCR, NGS, or IHC assays. Central assessment of MSI-H status using PCR (Idylla MSI) test and dMMR status using IHC (Omnis MMR) test was conducted retrospectively on patient tumor specimens used for local MSI-H/dMMR status determination. Patients with confirmed MSI-H/dMMR status by either central test comprised the primary study population.

The trial excluded patients with brain metastasis that were symptomatic, had active autoimmune disease, used systemic corticosteroids or immunosuppressants, or had been treated with checkpoint inhibitors.

Patients were randomized to receive one of the following treatments:

- OPDIVO 240 mg every 3 weeks and ipilimumab 1 mg/kg every 3 weeks for a maximum of 4 doses, then OPDIVO 480 mg every 4 weeks.
- OPDIVO 240 mg every 2 weeks for 6 doses, then OPDIVO 480 mg every 4 weeks.
- Investigator’s choice chemotherapy
  - mFOLFOX6 (oxaliplatin, leucovorin, and FU) with or without either bevacizumab or cetuximab: Oxaliplatin 85 mg/m^2, leucovorin 400 mg/m^2, and FU 400 mg/m^2 bolus followed by FU 2400 mg/m^2 over 46 hours every 2 weeks. Bevacizumab 5 mg/kg or cetuximab 500 mg/m^2 administered prior to mFOLFOX6 every 2 weeks.
  - FOLFIRI (irinotecan, leucovorin, and FU) with or without either bevacizumab or cetuximab: Irinotecan 180 mg/m^2, leucovorin 400 mg/m^2, and FU 400 mg/m^2 bolus and FU 2400 mg/m^2 over 46 hours every 2 weeks. Bevacizumab 5 mg/kg on or cetuximab 500 mg/m^2 administered prior to FOLFIRI every 2 weeks.

Randomization was stratified by tumor location (right vs left) and by prior lines of therapy (0, 1, 2L+). Patients randomized to the chemotherapy arm could receive OPDIVO in combination with ipilimumab upon progression assessed by BICR.

Study treatment was administered until disease progression, unacceptable toxicity, or for up to 2 years for patients who received OPDIVO plus ipilimumab or nivolumab monotherapy. Patients who discontinued combination therapy because of an adverse reaction attributed to ipilimumab were permitted to continue OPDIVO as a single agent. OPDIVO with or without ipilimumab could be administered beyond RECIST 1.1-assessed progressive disease if there was a clinical benefit as determined by investigator and therapy was tolerated. Tumor assessments per RECIST v1.1 were conducted every 6 weeks for the first 24 weeks, then every 8 weeks thereafter up until week 96, then every 16 weeks thereafter up until week 144, and then every 24 weeks.

The evaluation of efficacy relied on the comparison of patients with centrally confirmed MSI-H/dMMR mCRC randomized to OPDIVO in combination with ipilimumab versus chemotherapy in the first-line (1L) setting and the comparison of patients with centrally confirmed MSI-H/dMMR mCRC randomized to OPDIVO plus ipilimumab vs nivolumab in all lines setting.

The major efficacy outcome measure was BICR-assessed PFS per RECIST 1.1. Additional efficacy outcome measures included ORR and duration of response assessed by BICR and OS.

The baseline characteristics of the total of 839 patients randomized were: the median age was 63 years (range: 20 to 87), with 46% ≥65 years of age and 14% ≥75 years of age; 50% were male and 87% were White, 9.3% were Asian, 1.5% Black or African American, and 2.3% other race; 9.2% were Hispanic or Latino, 50% Not Hispanic or Latino, 41% ethnicity unknown. Baseline ECOG performance status was 0 (52%) and 1 (48%); number of prior lines of therapy was 0 (56%), 1 (24%), and ≥2 (19%); and tumor location was right-sided or left-sided for 69% and 31% of patients. The baseline characteristics in patients with centrally confirmed MSI-H/dMMR is consistent with that of all randomized patients.

First Line OPDIVO in combination with ipilimumab

Among 303 patients in the first-line setting who were randomly assigned to OPDIVO in combination with ipilimumab (202) and to chemotherapy (101), 171 and 84 patients had centrally confirmed MSI-H/dMMR status in OPDIVO in combination with ipilimumab arm and chemotherapy arm, respectively.

In the 1L setting 200 of 202 patients assigned to receive OPDIVO combined with ipilimumab and 88 of 101 patients assigned to receive chemotherapy received at least 1 dose of study treatment. Among the 88 patients who received chemotherapy, 58% and 42% of patients received oxaliplatin-containing regimens and irinotecan-containing regimens, respectively, and 66 (75%) patients received a targeted agent, either bevacizumab (64%) or cetuximab (11%).

The BICR-assessed PFS efficacy results for patients with centrally confirmed MSI-H/dMMR randomized to the OPDIVO and ipilimumab arm compared with chemotherapy in the 1L setting are presented in Table 76 and Figure 23. The comparative results of ORR and OS between arms were not available at the time of the PFS analysis due to statistical testing strategy.

Table 76: Efficacy Results, First Line - CHECKMATE-8HW
 | OPDIVO and Ipilimumab (n=171) | Chemotherapy (n=84)
Progression-free Survival
Disease progression or death (%) | 48 (28) | 52 (62)
Median in monthsb (95% CI) | NR; (38.4, NE) | 5.8; (4.4, 7.8)
Hazard ratioc (95% CI) | 0.21 (0.14, 0.32)
p-valuea | <0.0001
NR: Not Reached; NE: Not Estimable.
Minimum follow-up was 6.1 months at data cutoff date 12Oct2023.
a Based on log-rank test stratified by the same factors as used in the Cox proportional hazards model. The p-value threshold for statistical significance was 0.0209.
b Based on Kaplan-Meier estimates.
c HR from a Cox proportional hazards model stratified by tumor sidedness (left vs right) per IRT.

Figure 23: Progression-free Survival (First Line OPDIVO + Ipilimumab vs Chemotherapy) - CHECKMATE-8HW

All Lines OPDIVO in combination with ipilimumab

Among 707 patients across all treatment lines who were randomly assigned to OPDIVO in combination with ipilimumab (354) and to OPDIVO (353) single agent, 296 and 286 patients had centrally confirmed MSI-H/dMMR status in the OPDIVO in combination with ipilimumab arm and in the OPDIVO arm, respectively. Patients receiving at least 1 dose of study treatment included 352 of 354 patients randomized to OPDIVO in combination with ipilimumab, and 351 of 353 patients randomized to single agent OPDIVO.

The BICR-assessed PFS and ORR efficacy results for patients with centrally confirmed MSI-H/dMMR randomized to the OPDIVO in combination with ipilimumab compared with nivolumab single agent across all treatment lines setting are presented in Table 77 and Figure 24. The comparative results of OS between arms were not available at the time of the PFS analysis due to statistical testing strategy.

Table 77: Efficacy Results, All Lines - CHECKMATE-8HW
 | OPDIVO and Ipilimumab (n=296) | OPDIVO (n=286)
Progression-free Survival
Disease progression or death n (%) | 101 (34) | 136 (48)
Median (months)b (95% CI) | NR; (53.8, NE) | 39.3; (22.1, NE)
Hazard ratioc (95% CI) | 0.62 (0.48, 0.81)
p-valuea | 0.0003
Objective Response Rate (ORR)
Response Rate, n (%); (95% CI) | 209 (71%); (65, 76) | 165 (58%); (52, 63)
Complete Response Rate, n (%) | 90 (30%) | 80 (28%)
Partial Response Rate, n (%) | 119 (40%) | 85 (30%)
p-valued | 0.0011
NR: Not Reached; NE: Not Estimable.
Minimum follow-up was 16.7 months at data cutoff date 28Aug2024.
a Based on log-rank test stratified by the same factors as used in the Cox proportional hazards model. The p-value threshold for statistical significance was 0.0095.
b Based on Kaplan-Meier estimates.
c HR from a Cox proportional hazards model stratified by tumor sidedness (left vs right) and prior lines of therapy (0, 1, ≥2) per IRT.
d Based on Cochran-Mantel-Haenszel test stratified by the same factors as used in the Cox proportional hazards model. The p-value threshold for statistical significance was 0.006.

Figure 24: Progression-free Survival (All lines OPDIVO + Ipilimumab vs OPDIVO) - CHECKMATE-8HW

Treatment of MSI-H or dMMR mCRC after Progression Following Treatment with a Fluoropyrimidine, Oxaliplatin, and Irinotecan

CHECKMATE-142 (NCT02060188) was a multicenter, non-randomized, multiple parallel-cohort, open-label trial conducted in patients with locally determined dMMR or MSI-H metastatic CRC (mCRC) who had disease progression during or after prior treatment with fluoropyrimidine- , oxaliplatin- , or irinotecan-based chemotherapy. Key eligibility criteria were at least one prior line of treatment for metastatic disease, ECOG performance status 0 or 1, and absence of the following: active brain metastases, active autoimmune disease, or medical conditions requiring systemic immunosuppression.

Patients enrolled in the single agent OPDIVO MSI-H mCRC cohort received OPDIVO 3 mg/kg by intravenous infusion (IV) every 2 weeks. Patients enrolled in the OPDIVO and ipilimumab MSI-H mCRC cohort received OPDIVO 3 mg/kg and ipilimumab 1 mg/kg intravenously every 3 weeks for 4 doses, followed by OPDIVO as a single agent at a dose of 3 mg/kg as intravenous infusion every 2 weeks. Treatment in both cohorts continued until unacceptable toxicity or radiographic progression.

Tumor assessments were conducted every 6 weeks for the first 24 weeks and every 12 weeks thereafter. Efficacy outcome measures included ORR and DOR as assessed by BICR using RECIST v1.1.

A total of 74 patients were enrolled in the single-agent MSI-H mCRC OPDIVO cohort. The median age was 53 years (range: 26 to 79) with 23% ≥65 years of age and 5% ≥75 years of age, 59% were male and 88% were White. Baseline ECOG performance status was 0 (43%), 1 (55%), or 3 (1.4%) and 36% were reported to have Lynch Syndrome. Across the 74 patients, 72% received prior treatment with a fluoropyrimidine, oxaliplatin, and irinotecan; 7%, 30%, 28%, 19%, and 16% received 0, 1, 2, 3, or ≥4 prior lines of therapy for metastatic disease, respectively, and 42% of patients had received an anti-EGFR antibody.

A total of 119 patients were enrolled in the OPDIVO and ipilimumab MSI-H mCRC cohort. The median age was 58 years (range: 21 to 88), with 32% ≥65 years of age and 9% ≥75 years of age; 59% were male and 92% were White. Baseline ECOG performance status was 0 (45%) and 1 (55%), and 29% were reported to have Lynch Syndrome. Across the 119 patients, 69% had received prior treatment with a fluoropyrimidine, oxaliplatin, and irinotecan; 10%, 40%, 24%, and 15% received 1, 2, 3, or ≥4 prior lines of therapy for metastatic disease, respectively, and 29% had received an anti-EGFR antibody.

Efficacy results for each of these single-arm cohorts are shown in Table 78.

Table 78: Efficacy Results - CHECKMATE-142
 | OPDIVOa MSI-H/dMMR Cohort |  | OPDIVO and Ipilimumabb MSI-H/dMMR Cohort
 | All Patients (n=74) | Prior Treatment (Fluoropyrimidine, Oxaliplatin, and Irinotecan) (n=53) | All Patients (n=119) | Prior Treatment (Fluoropyrimidine, Oxaliplatin, and Irinotecan) (n=82)
Overall Response Rate per BICR; n (%) | 28 (38%) | 17 (32%) | 71 (60%) | 46 (56%)
(95% CI)c | (27, 50) | (20, 46) | (50, 69) | (45, 67)
Complete Response (%) | 8 (11%) | 5 (9%) | 17 (14%) | 11 (13%)
Partial Response (%) | 20 (27%) | 12 (23%) | 54 (45%) | 35 (43%)
Duration of Response
Proportion of responders with ≥6 months response duration | 86% | 94% | 89% | 87%
Proportion of responders with ≥12 months response duration | 82% | 88% | 77% | 74%
a Minimum follow-up 33.7 months for all patients treated with OPDIVO (n=74).
b Minimum follow-up 27.5 months for all patients treated with OPDIVO and ipilimumab (n=119).
c Estimated using the Clopper-Pearson method.

14.12 Hepatocellular Carcinoma

Treatment of Unresectable or Metastatic Hepatocellular Carcinoma (HCC)

CHECKMATE-9DW (NCT04039607) was a randomized (1:1), open-label trial in adults (18 years of age or older) with unresectable or metastatic HCC. Patients had histologically confirmed HCC, Child Pugh Class A, ECOG performance status 0 or 1, and no prior systemic therapy for advanced disease. Esophagogastroduodenoscopy was not mandated prior to enrollment. The trial excluded patients with active autoimmune disease, brain or leptomeningeal metastases, a history of hepatic encephalopathy (within 12 months of randomization), a platelet count <60,000, clinically significant ascites, medical conditions requiring systemic immunosuppression, infection with HIV, or active co-infection with hepatitis B virus (HBV) and hepatitis C virus (HCV) or HBV and hepatitis D virus (HDV).

Patients were randomized to receive either:

- OPDIVO 1 mg/kg administered intravenously over 30 minutes in combination with ipilimumab 3 mg/kg administered intravenously over 30 minutes every 3 weeks, for a maximum of 4 doses, followed by single agent OPDIVO at 480 mg administered intravenously over 30 minutes every 4 weeks, or
- Investigator’s choice:
  - Lenvatinib 8 mg orally daily (if body weight <60 kg) or 12 mg orally daily (if body weight ≥60 kg), or
  - Sorafenib 400 mg orally twice daily

Randomization was stratified by etiology (HBV vs. HCV vs. non-viral), macrovascular invasion and/or extrahepatic spread (present or absent), and alpha-fetoprotein levels (≥400 or <400 ng/mL). Study treatment for OPDIVO in combination with ipilimumab continued until disease progression, unacceptable toxicity, or up to 2 years. Patients who discontinued combination therapy because of an adverse reaction attributed to ipilimumab were permitted to continue OPDIVO as a single agent. Treatment beyond RECIST 1.1 defined disease progression was permitted if the patient was clinically stable and considered to be deriving clinical benefit by the investigator. Tumor assessments were performed at baseline, after randomization at week 9 and week 16, then every 8 weeks up to 48 weeks, and then every 12 weeks thereafter until disease progression, treatment discontinuation, or initiation of subsequent therapy. The primary efficacy outcome measure was OS in all randomized patients. Additional efficacy measures included BICR-assessed ORR and DOR based on RECIST 1.1 criteria.

A total of 668 patients were randomized to receive OPDIVO in combination with ipilimumab (n=335) or investigator’s choice (n=333) of lenvatinib or sorafenib. In the investigator arm, 85% and 15% of treated patients received lenvatinib or sorafenib, respectively. The trial population characteristics were median age 66 years (range: 20 to 89), with 53% ≥65 years old; 82% male; 53% White, 44% Asian, 2.2% Black; 12% Hispanic or Latino, 48% Not Hispanic or Latino, 40% not reported. Baseline ECOG performance status was 0 (71%) or 1 (29%). Thirty-four percent (34%) of patients had HBV infection, 28% had HCV infection, and 36% had no evidence of HBV or HCV infection.

Nineteen percent (19%) of patients had alcoholic liver disease and 11% had non-alcoholic fatty liver disease. The majority of patients had BCLC stage C (73%) disease at baseline, 19% had stage B, and 6% had stage A. Patients with Child-Pugh scores of 5, 6, and 7 were 77%, 20%, and 3%, respectively; 1 patient with Child Pugh 8 was enrolled. A total of 54% of patients had extrahepatic spread; 25% had macrovascular invasion; and 33% had AFP levels ≥400 µg/L.

CHECKMATE-9DW demonstrated a statistically significant improvement in OS and ORR. The minimum follow-up was 26.8 months. Efficacy results are shown in Table 79 and Figure 25.

Table 79: Efficacy Results - CHECKMATE-9DW
 | OPDIVO and Ipilimumab (n=335) | Lenvatinib or Sorafenib (n=333)
Overall Survival
Deaths (%) | 194 (58%) | 228 (68%)
Median (months); (95% CI) | 23.7; (18.8, 29.4) | 20.6; (17.5, 22.5)
Hazard ratio; (95% CI)a | 0.79; (0.65, 0.96)
p-valueb | 0.0180
Overall Response Rate, n (%)c | 121 (36.1) | 44 (13.2)
(95% CI) | (31.0, 41.5) | (9.8, 17.3)
p-valued | <0.0001
Complete response (%) | 23 (6.9) | 6 (1.8)
Partial response (%) | 98 (29.3) | 38 (11.4)
Duration of Response (months)c
Median; (95% CI) | 30.4; (21.2, NRe) | 12.9; (10.2, 31.2)
Range | 1.5+, 36.9+ | 2.1+, 32.5+
a Based on stratified Cox proportional hazard model.
b Based on a 2-sided stratified log-rank test. Boundary for statistical significance: p-value ≤0.0257.
c Assessed by BICR using RECIST 1.1.
d Based on a 2-sided stratified Cochran-Mantel-Haenszel test. Boundary for statistical significance: p-value ≤0.025.
e NR: Not Reached.
+ Censored observation.

Figure 25: Overall Survival - CHECKMATE-9DW

Previously Treated Hepatocellular Carcinoma

CHECKMATE-040 (NCT01658878) was a multicenter, multiple cohort, open-label trial that evaluated the efficacy of OPDIVO as a single agent and in combination with ipilimumab in patients with hepatocellular carcinoma (HCC) who progressed on or were intolerant to sorafenib. Additional eligibility criteria included histologic confirmation of HCC and Child-Pugh Class A cirrhosis. The trial excluded patients with active autoimmune disease, brain metastasis, a history of hepatic encephalopathy, clinically significant ascites, infection with HIV, or active co-infection with hepatitis B virus (HBV) and hepatitis C virus (HCV) or HBV and hepatitis D virus (HDV); however, patients with only active HBV or HCV were eligible.

Tumor assessments were conducted every 6 weeks for 48 weeks and then every 12 weeks thereafter. The major efficacy outcome measure was confirmed overall response rate as assessed by BICR using RECIST v1.1 and modified RECIST (mRECIST) for HCC. Duration of response was also assessed.

The efficacy of OPDIVO in combination with ipilimumab was evaluated in 49 patients (Cohort 4) who received OPDIVO 1 mg/kg and ipilimumab 3 mg/kg administered every 3 weeks for 4 doses, followed by single-agent OPDIVO at 240 mg every 2 weeks until disease progression or unacceptable toxicity. The median age was 60 years (range: 18 to 80), 88% were male, 74% were Asian, and 25% were White. Baseline ECOG performance status was 0 (61%) or 1 (39%). Fifty-seven (57%) percent of patients had active HBV infection, 8% had active HCV infection, and 35% had no evidence of active HBV or HCV. The etiology for HCC was alcoholic liver disease in 16% and non-alcoholic fatty liver disease in 6% of patients. Child-Pugh class and score was A5 for 82% and A6 for 18%; 80% of patients had extrahepatic spread; 35% had vascular invasion; and 51% had AFP levels ≥400 µg/L. Prior cancer treatment history included surgery (74%), radiotherapy (29%), or local treatment (59%). All patients had received prior sorafenib, of whom 10% were unable to tolerate sorafenib; 29% of patients had received 2 or more prior systemic therapies.

Efficacy results are shown in Table 80. The results for OPDIVO in combination with ipilimumab in Cohort 4 are based on a minimum follow-up of 28 months.

Table 80: Efficacy Results - Cohort 4 of CHECKMATE-040
 | OPDIVO and Ipilimumab (Cohort 4) (n=49)
Overall Response Rate per BICR,a n (%), RECIST v1.1 | 16 (33%)
(95% CI)b | (20, 48)
Complete response | 4 (8%)
Partial response | 12 (24%)
Duration of Response per BICR,a RECIST v1.1 | n=16
Range (months) | 4.6, 30.5+
Percent with duration ≥6 months | 88%
Percent with duration ≥12 months | 56%
Percent with duration ≥24 months | 31%
Overall Response Rate per BICR,a n (%), mRECIST | 17 (35%)
(95% CI)b | (22, 50)
Complete response | 6 (12%)
Partial response | 11 (22%)
a Confirmed by BICR.
b Confidence interval is based on the Clopper and Pearson method.

14.13 Esophageal Cancer

Adjuvant Treatment of Resected Esophageal or Gastroesophageal Junction Cancer

CHECKMATE-577 (NCT02743494) was a randomized, multicenter, double-blind trial in 794 patients with completely resected (negative margins) esophageal or gastroesophageal junction cancer who had residual pathologic disease following concurrent chemoradiotherapy (CRT). Patients were randomized (2:1) to receive either OPDIVO 240 mg or placebo by intravenous infusion over 30 minutes every 2 weeks for 16 weeks followed by 480 mg or placebo by intravenous infusion over 30 minutes every 4 weeks beginning at week 17. Treatment was until disease recurrence, unacceptable toxicity, or for up to 1 year in total duration. Enrollment required complete resection within 4 to 16 weeks prior to randomization. The trial excluded patients who did not receive CRT prior to surgery, had stage IV resectable disease, autoimmune disease, or any condition requiring systemic treatment with either corticosteroids (>10 mg daily prednisone or equivalent) or other immunosuppressive medications. Randomization was stratified by tumor PD-L1 status (≥1% vs. <1% or indeterminate or non-evaluable), pathologic lymph node status (positive ≥ypN1 vs. negative ypN0), and histology (squamous vs. adenocarcinoma). The major efficacy outcome measure was disease-free survival (DFS) defined as the time between the date of randomization and the date of first recurrence (local, regional, or distant from the primary resected site) or death, from any cause, whichever occurred first as assessed by the investigator prior to subsequent anti-cancer therapy. Patients on treatment underwent imaging for tumor recurrence every 12 weeks for 2 years, and a minimum of one scan every 6 to 12 months for years 3 to 5.

The trial population characteristics were: median age 62 years (range: 26 to 86), 36% were ≥65 years of age, 85% were male, 15% were Asian, 82% were White, and 1.1% were Black. Disease characteristics were AJCC Stage II (35%) or Stage III (65%) at initial diagnosis carcinoma, EC (60%) or GEJC (40%) at initial diagnosis, with pathologic positive lymph node status (58%) at study entry and histological confirmation of predominant adenocarcinoma (71%) or squamous cell carcinoma (29%). The baseline Tumor PD-L1 status ≥1% was positive for 16% of patients and negative for 72% of patients. Baseline ECOG performance status was 0 (58%) or 1 (42%).

CHECKMATE-577 demonstrated a statistically significant improvement in DFS for patients randomized to the OPDIVO arm as compared with the placebo arm. DFS benefit was observed regardless of tumor PD-L1 expression and histology.

Efficacy results are shown in Table 81 and Figure 26.

Table 81: Efficacy Results - CHECKMATE-577
 | OPDIVO (n=532) | Placebo (n=262)
Disease-free Survival
Number of events, n (%) | 241 (45%) | 155 (59%)
Median (months) (95% CI) | 22.4 (16.6, 34.0) | 11.0 (8.3, 14.3)
Hazard ratioa (95% CI) | 0.69 (0.56, 0.85)
p-valueb | 0.0003
a Based on a stratified proportional hazards model.
b Based on a stratified log-rank test.

Figure 26: Disease-free Survival - CHECKMATE-577

First-line Treatment of Unresectable Advanced or Metastatic ESCC Whose Tumors Express PD-L1 (≥1)

CHECKMATE-648 (NCT03143153) was a randomized, active-controlled, open-label trial in patients with previously untreated unresectable advanced, recurrent or metastatic ESCC (squamous or adenosquamous histology). The trial enrolled patients whose tumor was evaluable for tumor cell (TC) PD-L1 expression [also called PD-L1 tumor proportion score (TPS)], which was evaluated using the PD-L1 IHC 28-8 pharmDx assay at a central laboratory. A retrospective scoring of a patient’s tumor PD-L1 status using Combined Positive Score (CPS), was also conducted using the PD-L1-stained tumor specimens used for randomization. Patients were not amenable to chemoradiation or surgery with curative intent. Prior treatment with curative intent was allowed if completed more than six months prior to trial enrollment. The trial excluded patients with brain metastasis that were symptomatic, had active autoimmune disease, used systemic corticosteroids or immunosuppressants, or patients at high risk of bleeding or fistula due to apparent invasion of tumor to organs adjacent to the esophageal tumor. Patients were randomized to receive one of the following treatments:

- OPDIVO 240 mg on days 1 and 15, fluorouracil 800 mg/m^2/day intravenously on days 1 through 5 (for 5 days), and cisplatin 80 mg/m^2 intravenously on day 1 (of a 4-week cycle).
- OPDIVO 3 mg/kg every 2 weeks in combination with ipilimumab 1 mg/kg every 6 weeks.
- Fluorouracil 800 mg/m^2/day intravenously on days 1 through 5 (for 5 days), and cisplatin 80 mg/m^2 intravenously on day 1 (of a 4-week cycle).

Patients received OPDIVO until disease progression, unacceptable toxicity, or up to 2 years. In patients who received OPDIVO in combination with chemotherapy and in whom either fluorouracil and/or cisplatin were discontinued, other components of the treatment regimen were allowed to be continued. Patients who discontinued combination therapy because of an adverse reaction attributed to ipilimumab were permitted to continue OPDIVO as a single agent.

Randomization was stratified by TC PD-L1 expression (≥1% vs. <1% or indeterminate), region (East Asia vs. Rest of Asia vs. Rest of World), ECOG performance status (0 vs. 1), and number of organs with metastases (≤1 vs. ≥2). The major efficacy outcome measures were OS and BICR-assessed PFS in patients with TC PD-L1 expression ≥ 1%. Additional efficacy measures included OS in all randomized patients, BICR-assessed PFS in all randomized patients, and ORR assessed by BICR in TC PD-L1 expression ≥ 1% and in all randomized patients. The tumor assessments per RECIST v1.1 were conducted every 6 weeks up to and including week 48, then every 12 weeks thereafter.

A total of 970 patients were randomized in the CHECKMATE-648 study, among whom 965 and 906 patients had quantifiable TC PD-L1 expression and CPS at baseline, respectively; 85% (824/970) had tumors with PD-L1 CPS ≥1. The trial population characteristics in patients with PD-L1 CPS ≥1 were: median age 63 years (range: 26 to 90), 46% were ≥65 years of age, 82% were male, 71% were Asian, 25% were White, and 1.2% were Black or African American. Patients had histological confirmation of squamous cell carcinoma (99%) or adenosquamous cell carcinoma (1.7%) in the esophagus. Baseline ECOG performance status was 0 (44.0%) or 1 (54%).

A statistically significant improvement in OS was demonstrated in patients randomized to OPDIVO in combination with chemotherapy and patients randomized to OPDIVO in combination with ipilimumab compared with chemotherapy. An exploratory analysis of OS in patients with PD-L1 CPS <1 showed a HR of 0.98 (95% CI 0.50, 1.95) for the comparison of OPDIVO in combination with chemotherapy, and the exploratory analysis OS in patients with PD-L1 CPS <1 showed a HR of 1.0 (95% CI 0.52, 1.94) for the comparison of OPDIVO in combination with ipilimumab; these results indicate that the improvement in the ITT population was primarily attributed to the results observed in the subgroup of patients with PD-L1 CPS ≥1. Efficacy results are shown in Table 82 and Figures 27 and 28.

Table 82: Efficacy Results - CHECKMATE-648
 | OPDIVO with Cisplatin and Fluorouracil (n=158) | OPDIVO and Ipilimumab (n=158) | Cisplatin and Fluorouracil (n=157) | OPDIVO with Cisplatin and Fluorouracil (n=278) | OPDIVO and Ipilimumab (n=266) | Cisplatin and Fluorouracil (n=280)
 | TC PD-L1 expression ≥1% |  |  | PD-L1 CPS ≥1
Overall Survival
Deaths (%) | 98 (62) | 106 (67) | 121 (77) | 177 (64) | 179 (67) | 205 (73)
Median (months); (95% CI) | 15.4; (11.9, 19.5) | 13.7; (11.2, 17.0) | 9.1; (7.7, 10) | 13.8; (12.0, 16.1) | 12.7; (10.9, 15.5) | 9.8; (8.8, 11.6)
Hazard ratio (95% CI)b | 0.54; (0.41, 0.71) | 0.64; (0.49, 0.84) | - | 0.69; (0.57, 0.85) | 0.76; (0.62, 0.93) | -
p-valuec | <0.0001S1 | 0.0010S2 | - | - | - | -
Progression-free Survivala
Disease progression or death (%) | 117 (74) | 123 (78) | 100 (64) | 201 (72) | 206 (77) | 184 (66)
Median (months); (95% CI) | 6.9; (5.7, 8.3) | 4.0; (2.4, 4.9) | 4.4; (2.9, 5.8) | 5.8; (5.5, 7.0) | 2.8; (2.6, 4.2) | 5.6; (4.2, 5.9)
Hazard ratio; (95% CI)b | 0.65; (0.49, 0.86) | 1.02; (0.78, 1.34) | - | 0.8; (0.7, 1.0) | 1.2; (1.0, 1.5) | -
p-valuec | 0.0023S3 | NS | - | - | - | -
Overall Response Rate, n (%)a, NT | 84 (53.2) | 56 (35.4) | 31 (19.7) | 135 (49) | 74 (28) | 76 (27)
(95% CI) | (45.1, 61.1) | (28.0, 43.4) | (13.8, 26.8) | (42.5, 54.6) | (22.5, 33.6) | (22.0, 32.8)
Complete response (%) | 26 (16.5) | 28 (17.7) | 8 (5.1) | 39 (14) | 32 (12.0) | 18 (6.4)
Partial response (%) | 58 (36.7) | 28 (17.7) | 23 (14.6) | 96 (35) | 42 (15.8) | 58 (20.7)
Duration of Response (months)a
Median; (95% CI) | 8.4; (6.9, 12.4) | 11.8; (7.1, 27.4) | 5.7; (4.4, 8.7) | 8.2; (6.7, 11.1) | 11.8; (7.1, 23.6) | 6.9; (5.7, 8.2)
Range | 1.4+, 34.6 | 1.4+, 34.5+ | 1.4+, 31.8+ | 1.4+, 35.9+ | 1.4+, 34.5+ | 1.4+, 31.8+
a Assessed by BICR.
b Based on stratified Cox proportional hazard model. Hazard ratios are reported for each OPDIVO containing arm compared to chemotherapy within each analysis population.
c Based on a stratified 2-sided log-rank test.
S1, S2, S3 Significant p-value compared to stopping boundary of 0.005, 0.014, and 0.015 respectively.
NS: Not Statistically significant, NT: Not evaluated for statistical significance as per pre-specified hierarchical testing procedure.

Figure 27: Overall Survival – CHECKMATE-648

(A) OS in CPS ≥1

(B) OS in TC PD-L1 ≥1%

Figure 28: Progression-free Survival – CHECKMATE-648

(A) PFS in CPS ≥1

(B) PFS in TC PD-L1 ≥1%

Previously Treated Unresectable Advanced, Recurrent or Metastatic Esophageal Squamous Cell Carcinoma (ESCC)

ATTRACTION-3 (NCT02569242) was a multicenter, randomized (1:1), active-controlled, open-label trial in patients with unresectable advanced, recurrent, or metastatic ESCC, who were refractory or intolerant to at least one fluoropyrimidine- and platinum-based regimen. The trial enrolled patients regardless of PD-L1 status, but tumor specimens were evaluated prospectively using the PD-L1 IHC 28-8 pharmDx assay at a central laboratory. The trial excluded patients who were refractory or intolerant to taxane therapy, had brain metastases that were symptomatic or required treatment, had autoimmune disease, used systemic corticosteroids or immunosuppressants, or had apparent tumor invasion of organs adjacent to the esophageal tumor or had stents in the esophagus or respiratory tract. Patients were randomized to receive OPDIVO 240 mg by intravenous infusion over 30 minutes every 2 weeks or investigator’s choice of taxane chemotherapy consisting of docetaxel (75 mg/m^2 intravenously every 3 weeks) or paclitaxel (100 mg/m^2 intravenously once a week for 6 weeks followed by 1 week off).

Randomization was stratified by region (Japan vs. Rest of World), number of organs with metastases (≤1 vs. ≥2), and PD-L1 status (≥1% vs. <1% or indeterminate). Patients were treated until disease progression, assessed by the investigator per RECIST v1.1, or unacceptable toxicity. The tumor assessments were conducted every 6 weeks for 1 year, and every 12 weeks thereafter. The major efficacy outcome measure was OS. Additional efficacy outcome measures were ORR and PFS as assessed by the investigator using RECIST v1.1 and DOR.

A total of 419 patients were randomized; 210 to the OPDIVO arm and 209 to the investigator’s choice arm (docetaxel: 31%, paclitaxel: 69%). The trial population characteristics were: median age 65 years (range: 33 to 87), 53% were ≥65 years of age, 87% were male, 96% were Asian and 4% were White. Sixty-seven percent of patients had received one prior systemic therapy regimen and 26% had received two prior systemic therapy regimens prior to enrolling in ATTRACTION-3. Baseline ECOG performance status was 0 (50%) or 1 (50%).

ATTRACTION-3 demonstrated a statistically significant improvement in OS for patients randomized to OPDIVO as compared with investigator’s choice of taxane chemotherapy. OS benefit was observed regardless of PD-L1 expression level. OS results by PD-L1 CPS level (<1 and ≥1) were not studied. The minimum follow-up was 17.6 months. Efficacy results are shown in Table 83 and Figure 29.

Table 83: Efficacy Results - ATTRACTION-3
 | OPDIVO (n=210) | Docetaxel or Paclitaxel (n=209)
Overall Survivala
Deaths (%) | 160 (76%) | 173 (83%)
Median (months) (95% CI) | 10.9 (9.2, 13.3) | 8.4 (7.2, 9.9)
Hazard ratio (95% CI)b | 0.77 (0.62, 0.96)
p-valuec | 0.0189
Overall Response Rated | 33 (19.3) | 34 (21.5)
(95% CI) | (13.7, 26.0) | (15.4, 28.8)
Complete response (%) | 1 (0.6) | 2 (1.3)
Partial response (%) | 32 (18.7) | 32 (20.3)
Median duration of response (months) (95% CI) | 6.9 (5.4, 11.1) | 3.9 (2.8, 4.2)
p-valuee | 0.6323
Progression-free Survivala, f
Disease progression or death (%) | 187 (89) | 176 (84)
Median (months) (95% CI) | 1.7 (1.5, 2.7) | 3.4 (3.0, 4.2)
Hazard ratio (95% CI)b | 1.1 (0.9, 1.3)
a Based on ITT analysis
b Based on a stratified proportional hazards model.
c Based on a stratified log-rank test.
d Based on Response Evaluable Set (RES) analysis, n=171 in OPDIVO group and n=158 in investigator’s choice group.
e Based on stratified Cochran-Mantel-Haenszel test; p-value not significant.
f PFS not tested due to pre-specified hierarchical testing strategy.

Figure 29: Overall Survival - ATTRACTION-3

Of the 419 patients, 48% had PD-L1 positive ESCC, defined as ≥1% of tumor cells expressing PD-L1. The remaining 52% had PD-L1 negative ESCC defined as <1% of tumor cells expressing PD-L1.

In a pre-specified exploratory analysis by PD-L1 status, the hazard ratio (HR) for OS was 0.69 (95% CI: 0.51, 0.94) with median survivals of 10.9 and 8.1 months for the OPDIVO and investigator’s choice arms, respectively, in the PD-L1 positive subgroup. In the PD-L1 negative subgroup, the HR for OS was 0.84 (95% CI: 0.62, 1.14) with median survivals of 10.9 and 9.3 months for the OPDIVO and investigator’s choice arms, respectively.

14.14 Gastric Cancer, Gastroesophageal Junction Cancer, and Esophageal Adenocarcinoma Whose Tumors Express PD-L1 (≥1)

CHECKMATE-649 (NCT02872116) was a randomized, multicenter, open-label trial in patients (n=1581) with previously untreated advanced or metastatic gastric cancer, gastroesophageal junction cancer, and esophageal adenocarcinoma. The trial enrolled patients regardless of PD-L1 status, and tumor specimens were evaluated using the PD-L1 IHC 28-8 pharmDx assay at a central laboratory (tumor cell [TC] and Combined Positive Score [CPS]). The trial excluded patients who were known human epidermal growth factor receptor 2 (HER2) positive, or had untreated CNS metastases. Patients were randomized to receive OPDIVO in combination with chemotherapy (n=789) or chemotherapy (n=792). Patients received one of the following treatments:

- OPDIVO 240 mg in combination with mFOLFOX6 (fluorouracil, leucovorin and oxaliplatin) every 2 weeks or mFOLFOX6 every 2 weeks.
- OPDIVO 360 mg in combination with CapeOX (capecitabine and oxaliplatin) every 3 weeks or CapeOX every 3 weeks.

Patients were treated until disease progression, unacceptable toxicity, or up to 2 years. In patients who received OPDIVO in combination with chemotherapy and in whom chemotherapy was discontinued, OPDIVO monotherapy was allowed to be given at 240 mg every 2 weeks, 360 mg every 3 weeks, or 480 mg every 4 weeks up to 2 years after treatment initiation.

Randomization was stratified by tumor cell PD-L1 status (≥1% vs. <1% or indeterminate), region (Asia vs. US vs. Rest of World), ECOG performance status (0 vs. 1), and chemotherapy regimen (mFOLFOX6 vs. CapeOX). The major efficacy outcome measures, assessed in patients with PD-L1 CPS ≥5, were PFS assessed by BICR and OS. Additional efficacy outcome measures included OS and PFS in patients with PD-L1 CPS ≥1 and in all randomized patients, and ORR and DOR as assessed by BICR in patients with PD-L1 CPS ≥1 and ≥5, and in all randomized patients. Tumor assessments were conducted per RECIST v1.1 every 6 weeks up to and including week 48, then every 12 weeks thereafter.

A total of 1581 patients were randomized in the CHECKMATE-649 study, among whom 1296 and 955 had baseline PD-L1 CPS ≥1 and CPS ≥5 respectively. The trial population characteristics in patients with PD-L1 CPS ≥1 were: median age 62 years (range: 18 to 90), 40% were ≥65 years of age, 72% were male, 23% were Asian, and 69% were White, and 1% were Black or African American. Baseline ECOG performance status was 0 (42%) or 1 (58%). Seventy percent of patients had adenocarcinoma tumors in the stomach, 17% in the gastroesophageal junction, and 13% in the esophagus.

CHECKMATE-649 demonstrated a statistically significant improvement in OS and PFS for patients with PD-L1 CPS ≥5. Statistically significant improvement in OS was also demonstrated for all randomized patients and patients with PD-L1 CPS ≥1. Exploratory analysis of OS in the CPS <1 population showed a hazard ratio of 0.85 (95% CI: 0.63, 1.15), indicating that the improvement in the ITT population was primarily attributed to the results observed in the subgroup of patients with PD-L1 CPS ≥1. The minimum follow-up was 12.1 months. Efficacy results are shown in Table 84 and Figures 30, and 31.

Table 84: Efficacy Results - CHECKMATE-649
 | OPDIVO and mFOLFOX6 or CapeOX (n=641) | mFOLFOX6 or CapeOX (n=655) | OPDIVO and mFOLFOX6 or CapeOX (n=473) | mFOLFOX6 or CapeOX (n=482)
 | PD-L1 CPS ≥1 |  | PD-L1 CPS ≥5
Overall Survival
Deaths (%) | 434 (68) | 492 (75) | 309 (65) | 362 (75)
Median (months) (95% CI) | 14.0 (12.6, 15.0) | 11.3 (10.6, 12.3) | 14.4 (13.1, 16.2) | 11.1 (10.0, 12.1)
Hazard ratio (95% CI)a | 0.77 (0.68, 0.88) |  | 0.71 (0.61, 0.83)
p-valueb | <0.0001 |  | <0.0001
Progression-free Survivalc
Disease progression or death (%) | 454 (70.8) | 472 (72.1) | 328 (69.3) | 350 (72.6)
Median (months) (95% CI) | 7.5 (7.0, 8.4) | 6.9 (6.1, 7.0) | 7.7 (7.0, 9.2) | 6.0 (5.6, 6.9)
Hazard ratio; (95% CI)a | 0.74 (0.65, 0.85) |  | 0.68 (0.58, 0.79)
p-valueb | e |  | <0.0001
Overall Response Rate, n (%)c,d | 314 (49) | 249 (38) | 237 (50) | 184 (38)
(95% CI) | (45, 53) | (34, 42) | (46, 55) | (34, 43)
Complete response (%) | 65 (10) | 42 (6) | 55 (12) | 34 (7)
Partial response (%) | 249 (39) | 207 (32) | 182 (38) | 150 (31)
Duration of Response (months)c,d
Median (95% CI) Range | 8.5 (7.7, 10.3) 1.1+, 29.6+ | 6.9 (5.8, 7.6) 1.2+, 30.8+ | 9.5 (8.1, 11.9) 1.1+, 29.6+ | 6.9 (5.6, 7.9) 1.2+, 30.8+
a Based on stratified Cox proportional hazard model.
b Based on stratified log-rank test.
c Assessed by BICR.
d Based on confirmed response.
e Not evaluated for statistical significance.

Figure 30: Overall Survival (PD-L1 CPS ≥1) - CHECKMATE-649

Figure 31: Overall Survival (PD-L1 CPS ≥5) - CHECKMATE-649

An exploratory analysis of OS in the 44 patients with MSI-H tumors showed a HR of 0.37 (95% CI: 0.16, 0.87).

16 HOW SUPPLIED/STORAGE AND HANDLING

OPDIVO® (nivolumab) Injection is a clear to opalescent, colorless to pale-yellow solution in a single-dose vial available as follows:

Carton Contents | NDC
40 mg/4 mL (10 mg/mL) single-dose vial | 0003-3772-11
100 mg/10 mL (10 mg/mL) single-dose vial | 0003-3774-12
120 mg/12 mL (10 mg/mL) single-dose vial | 0003-3756-14
240 mg/24 mL (10 mg/mL) single-dose vial | 0003-3734-13

Store under refrigeration at 2°C to 8°C (36°F to 46°F). Protect from light by storing in the original package until time of use. Do not freeze or shake.

17 PATIENT COUNSELING INFORMATION

Advise the patient to read the FDA-approved patient labeling (Medication Guide).

Immune-Mediated Adverse Reactions

Inform patients of the risk of immune-mediated adverse reactions that may require corticosteroid treatment and withholding or discontinuation of OPDIVO, including:

- Pneumonitis: Advise patients to contact their healthcare provider immediately for any new or worsening cough, chest pain, or shortness of breath [see Warnings and Precautions (5.1)].
- Colitis: Advise patients to contact their healthcare provider immediately for diarrhea or severe abdominal pain [see Warnings and Precautions (5.1)].
- Hepatitis: Advise patients to contact their healthcare provider immediately for jaundice, severe nausea or vomiting, pain on the right side of abdomen, lethargy, or easy bruising or bleeding [see Warnings and Precautions (5.1)].
- Endocrinopathies: Advise patients to contact their healthcare provider immediately for signs or symptoms of hypophysitis, adrenal insufficiency, hypothyroidism, hyperthyroidism, and diabetes mellitus [see Warnings and Precautions (5.1)].
- Nephritis and Renal Dysfunction: Advise patients to contact their healthcare provider immediately for signs or symptoms of nephritis including decreased urine output, blood in urine, swelling in ankles, loss of appetite, and any other symptoms of renal dysfunction [see Warnings and Precautions (5.1)].
- Skin Adverse Reactions: Advise patients to contact their healthcare provider immediately for rash [see Warnings and Precautions (5.1)].

Infusion-Related Reactions

- Advise patients of the potential risk of infusion-related reactions [see Warnings and Precautions (5.2)].

Complications of Allogeneic HSCT

- Advise patients of potential risk of post-transplant complications [see Warnings and Precautions (5.3)].

Embryo-Fetal Toxicity

- Advise females of reproductive potential of the potential risk to a fetus and to inform their healthcare provider of a known or suspected pregnancy [see Warnings and Precautions (5.4), Use in Specific Populations (8.1)].
- Advise females of reproductive potential to use effective contraception during treatment with OPDIVO and for at least 5 months following the last dose [see Use in Specific Populations (8.3)].

Lactation

- Advise women not to breastfeed during treatment with OPDIVO and for 5 months after the last dose [see Use in Specific Populations (8.2)].

Manufactured by:
Bristol-Myers Squibb Company
Princeton, NJ 08543 USA
U.S. License No. 1713

MEDICATION GUIDE
OPDIVO® (op-DEE-voh)
(nivolumab)
injection

Read this Medication Guide before you start receiving OPDIVO and before each infusion. There may be new information. If your healthcare provider prescribes OPDIVO in combination with ipilimumab, also read the Medication Guide that comes with ipilimumab. If your healthcare provider prescribes OPDIVO in combination with cabozantinib, also read the Patient Information that comes with cabozantinib. This Medication Guide does not take the place of talking with your healthcare provider about your medical condition or your treatment.

What is the most important information I should know about OPDIVO?

OPDIVO is a medicine that may treat certain cancers by working with your immune system. OPDIVO can cause your immune system to attack normal organs and tissues in any area of your body and can affect the way they work. These problems can sometimes become severe or life-threatening and can lead to death. These problems may happen anytime during treatment or even after your treatment has ended. You may have more than one of these problems at the same time. Some of these problems may happen more often when OPDIVO is used in combination with another therapy.

Call or see your healthcare provider right away if you develop any new or worsening signs or symptoms, including:

Lung problems.

- cough

- shortness of breath

- chest pain

Intestinal problems.

- diarrhea (loose stools) or more frequent bowel movements than usual
- stools that are black, tarry, sticky, or have blood or mucus
- severe stomach-area (abdominal) pain or tenderness

Liver problems.

- yellowing of your skin or the whites of your eyes
- severe nausea or vomiting
- pain on the right side of your stomach area (abdomen)

- dark urine (tea colored)
- bleeding or bruising more easily than normal

Hormone gland problems.

- headaches that will not go away or unusual headaches
- eye sensitivity to light
- eye problems
- rapid heartbeat
- increased sweating
- extreme tiredness
- weight gain or weight loss
- feeling more hungry or thirsty than usual

- urinating more often than usual
- hair loss
- feeling cold
- constipation
- your voice gets deeper
- dizziness or fainting
- changes in mood or behavior, such as decreased sex drive, irritability, or forgetfulness

Kidney problems.

- decrease in your amount of urine
- blood in your urine

- swelling of your ankles
- loss of appetite

Skin problems.

- rash
- itching
- skin blistering or peeling
- swollen lymph nodes

- painful sore or ulcers in mouth or nose, throat, or genital area
- fever or flu-like symptoms

Problems can also happen in other organs and tissues. These are not all of the signs and symptoms of immune system problems that can happen with OPDIVO. Call or see your healthcare provider right away for any new or worsening signs or symptoms, which may include:

- chest pain, irregular heartbeat, shortness of breath or swelling of ankles
- confusion, sleepiness, memory problems, changes in mood or behavior, stiff neck, balance problems, tingling or numbness of the arms or legs
- double vision, blurry vision, sensitivity to light, eye pain, changes in eyesight
- persistent or severe muscle pain or weakness, muscle cramps
- low red blood cells, bruising

Rejection of a transplanted organ or tissue. Your healthcare provider should tell you what signs and symptoms you should report and monitor you depending on the type of organ transplant that you have had.

Getting medical treatment right away may help keep these problems from becoming more serious. Your healthcare provider will check you for these problems during treatment with OPDIVO. Your healthcare provider may treat you with corticosteroid or hormone replacement medicines. Your healthcare provider may also need to delay or completely stop treatment with OPDIVO, if you have severe side effects.

What is OPDIVO?

OPDIVO is a prescription medicine used to treat:

- adults and children 12 years of age and older with a type of skin cancer called melanoma.
  ∘ OPDIVO may be used alone or in combination with ipilimumab to treat melanoma that has spread or cannot be removed by surgery (advanced melanoma), or
  ∘ OPDIVO may be used alone to help prevent Stage IIB, Stage IIC, Stage III or Stage IV melanoma from coming back after it has been completely removed by surgery.
- adults with a type of lung cancer called non-small cell lung cancer (NSCLC).
  ∘ OPDIVO may be used in combination with chemotherapy that contains platinum and another chemotherapy medicine before you have surgery for early-stage NSCLC,
  ∘ OPDIVO may be used in combination with chemotherapy that contains platinum and another chemotherapy medicine before you have surgery for early-stage NSCLC:
    - that does not have an abnormal EGFR or ALK gene, and
    - then may be continued alone after surgery to help prevent your lung cancer from coming back.
  ∘ OPDIVO may be used in combination with ipilimumab as your first treatment for NSCLC:
    - when your lung cancer has spread to other parts of your body (metastatic), and
    - your tumors are positive for PD-L1, but do not have an abnormal EGFR or ALK gene.
  ∘ OPDIVO may be used in combination with ipilimumab and 2 cycles of chemotherapy that contains platinum and another chemotherapy medicine, as the first treatment of your NSCLC when your lung cancer:
    - has spread, or comes back, and
    - your tumor does not have an abnormal EGFR or ALK gene.
  ∘ OPDIVO may be used when your lung cancer:
    - has spread, and
    - you have received chemotherapy that contains platinum, and it did not work or is no longer working, and
    - if your tumor has an abnormal EGFR or ALK gene, you should have also received an EGFR or ALK inhibitor medicine and it did not work or is no longer working.
- adults with a type of cancer that affects the lining of the lungs and chest wall called malignant pleural mesothelioma.
  ∘ OPDIVO may be used in combination with ipilimumab as your first treatment for malignant pleural mesothelioma that cannot be removed by surgery.
- adults with a type of kidney cancer called renal cell carcinoma (RCC).
  ∘ OPDIVO may be used in combination with ipilimumab as your first treatment for certain people when your cancer has spread (advanced RCC).
  ∘ OPDIVO may be used in combination with cabozantinib as your first treatment when your cancer has spread (advanced RCC).
  ∘ OPDIVO may be used alone when your cancer has spread after treatment with other cancer medicines.
- adults with a type of blood cancer called classical Hodgkin lymphoma (cHL).
  ∘ OPDIVO may be used if:
    - your cancer has come back or spread after a type of stem cell transplant that uses your own stem cells (autologous), and
    - you used the medicine brentuximab vedotin before or after your stem cell transplant, or you received at least 3 kinds of treatment including a stem cell transplant that uses your own stem cells (autologous).
- adults with head and neck cancer (squamous cell carcinoma).
  ∘ OPDIVO may be used when your head and neck cancer:
    - has come back or spread, and
    - you have received chemotherapy that contains platinum and it did not work or is no longer working.
- adults with a type of cancer of the lining of the urinary tract called urothelial carcinoma (UC).
  ∘ OPDIVO may be used to help prevent cancer of the urinary tract from coming back after it was removed by surgery.
  ∘ OPDIVO may be used in combination with chemotherapy medicines cisplatin and gemcitabine as your first treatment when your urinary tract cancer has spread or cannot be removed by surgery.
  ∘ OPDIVO may be used when your urinary tract cancer has spread (locally advanced or metastatic), and:
    - you have received chemotherapy that contains platinum, and it did not work or is no longer working, or
    - your cancer worsened within 12 months of treatment with chemotherapy that contains platinum, either before or after surgery to remove your cancer.
- adults and children 12 years of age and older, with a type of colon or rectal cancer (colorectal cancer).
  ∘ OPDIVO may be used in combination with ipilimumab when your colon or rectal cancer:
    - cannot be removed with surgery, or has spread, and
    - is microsatellite instability-high (MSI-H) or mismatch repair deficient (dMMR).
  ∘ OPDIVO may be used alone when your colon or rectal cancer:
    - has spread, and
    - is microsatellite instability-high (MSI-H) or mismatch repair deficient (dMMR), and
    - you have received treatment with a fluoropyrimidine, oxaliplatin, and irinotecan, and it did not work or is no longer working.
- adults with a type of liver cancer called hepatocellular carcinoma (HCC).
  ∘ OPDIVO may be used in combination with ipilimumab as your first treatment when your liver cancer:
    - cannot be removed by surgery, or
    - has spread.
  ∘ OPDIVO may be used in combination with ipilimumab when your liver cancer:
    - cannot be removed by surgery, or
    - has spread, and
    - you have received prior treatment with sorafenib.
- adults with cancer of the tube that connects your throat to your stomach (esophageal cancer).
  ∘ OPDIVO may be used to help prevent your esophageal or gastroesophageal junction cancer from coming back when:
    - your esophageal or gastroesophageal junction cancer has been treated with chemoradiation followed by surgery to completely remove the cancer, but
    - some cancer cells were still present in the removed tumor or lymph nodes.
  ∘ OPDIVO may be used in combination with chemotherapy that contains fluoropyrimidine and platinum as your first treatment when your esophageal cancer:
    - is a type called squamous cell carcinoma, and
    - cannot be removed with surgery, or has spread, and
    - your tumors are positive for PD-L1.
  ∘ OPDIVO may be used in combination with ipilimumab as your first treatment when your esophageal cancer:
    - is a type called squamous cell carcinoma, and
    - cannot be removed with surgery, or has spread, and
    - your tumors are positive for PD-L1.
  ∘ OPDIVO may be used alone when your esophageal cancer:
    - is a type called squamous cell carcinoma, and
    - cannot be removed with surgery, and has come back or spread, and
    - you have received chemotherapy that contains fluoropyrimidine and platinum.
- adults with cancer of the stomach (gastric cancer), cancer where the esophagus joins the stomach (gastroesophageal junction cancer), and in adults with esophageal adenocarcinoma.
  ∘ OPDIVO may be used in combination with chemotherapy that contains fluoropyrimidine and platinum when your gastric, gastroesophageal junction, or esophageal cancer:
    - cannot be removed with surgery, or has spread, and
    - your tumors are positive for PD-L1.

It is not known if OPDIVO is safe and effective in children younger than 12 years of age with melanoma or MSI-H or dMMR metastatic colorectal cancer.

It is not known if OPDIVO is safe and effective in children for the treatment of any other cancers.

Before receiving OPDIVO, tell your healthcare provider about all of your medical conditions, including if you:

- have immune system problems such as Crohn’s disease, ulcerative colitis, or lupus.
- have received an organ transplant, including corneal transplant
- have received or plan to receive a stem cell transplant that uses donor stem cells (allogeneic)
- have received radiation treatment to your chest area in the past and have received other medicines that are like OPDIVO
- have a condition that affects your nervous system, such as myasthenia gravis or Guillain-Barré syndrome
- are pregnant or plan to become pregnant. OPDIVO can harm your unborn baby.
  Females who are able to become pregnant:
  ∘ Your healthcare provider should do a pregnancy test before you start receiving OPDIVO.
  ∘ You should use an effective method of birth control during treatment and for 5 months after your last dose of OPDIVO. Talk to your healthcare provider about birth control methods that you can use during this time.
  ∘ Tell your healthcare provider right away if you become pregnant during treatment with OPDIVO.
- are breastfeeding or plan to breastfeed. It is not known if OPDIVO passes into your breast milk. Do not breastfeed during treatment and for 5 months after your last dose of OPDIVO.

Tell your healthcare provider about all the medicines you take, including prescription and over-the-counter medicines, vitamins, and herbal supplements.

How will I receive OPDIVO?

- Your healthcare provider will give you OPDIVO into your vein through an intravenous (IV) line over 30 minutes.
- When OPDIVO is used alone, it is usually given every 2 weeks or 4 weeks depending on the dose you are receiving.
- When OPDIVO is used in combination with ipilimumab (except for treating NSCLC), OPDIVO is usually given every 3 weeks, for up to 4 doses. Ipilimumab will be given on the same day. After that, OPDIVO will be given alone every 2 weeks or 4 weeks depending on the dose you are receiving.
- For NSCLC before you have surgery, OPDIVO is given in combination with platinum-containing chemotherapy and another chemotherapy medicine every 3 weeks for 3 cycles. In some cases, OPDIVO is used in combination with chemotherapy every 3 weeks for up to 4 cycles before you have surgery, followed by OPDIVO used alone every 4 weeks after you have surgery for up to 1 year.
- For NSCLC that has spread to other parts of your body, when OPDIVO is used in combination with ipilimumab, OPDIVO is given every 3 weeks, and ipilimumab is given every 6 weeks for up to 2 years. Your healthcare provider will determine if you will also need to receive chemotherapy every 3 weeks for 2 cycles.
- For malignant pleural mesothelioma, OPDIVO is given every 3 weeks and ipilimumab is given every 6 weeks for up to 2 years.
- For RCC, when used in combination with cabozantinib, OPDIVO is usually given every 2 weeks or 4 weeks depending on the dose you are receiving. Cabozantinib is given once daily by mouth.
- For UC that has spread to other parts of your body or cannot be removed by surgery, when OPDIVO is used in combination with chemotherapy medicines cisplatin and gemcitabine, OPDIVO is given every 3 weeks for up to 6 cycles. Chemotherapy will be given on the same day. After that, OPDIVO will be given alone every 2 weeks or 4 weeks depending on the dose you are receiving.
- When OPDIVO is used in combination with fluoropyrimidine- and platinum-containing chemotherapy for treating esophageal squamous cell carcinoma (ESCC), OPDIVO is given either every 2 weeks or every 4 weeks, for up to 2 years.
- When OPDIVO is used in combination with ipilimumab for esophageal squamous cell carcinoma, OPDIVO is given every 2 weeks or 3 weeks and ipilimumab is given every 6 weeks for up to 2 years.
- For gastric cancer, gastroesophageal junction cancer and esophageal adenocarcinoma, when used in combination with fluoropyrimidine and platinum-containing chemotherapy, OPDIVO is given every 2 weeks or 3 weeks depending on the dose you are receiving, for up to 2 years. Chemotherapy will be given on the same day.
- Your healthcare provider will decide how many treatments you need.
- Your healthcare provider will do blood tests to check you for side effects.
- If you miss any appointments, call your healthcare provider as soon as possible to reschedule your appointment.

What are the possible side effects of OPDIVO?

OPDIVO can cause serious side effects, including:

- See “What is the most important information I should know about OPDIVO?”
- Severe infusion reactions. Tell your healthcare provider or nurse right away if you get these symptoms during an infusion of OPDIVO:

∘ chills or shaking
∘ itching or rash
∘ flushing
∘ shortness of breath or wheezing

∘ dizziness
∘ feel like passing out
∘ fever
∘ back or neck pain

- Complications of stem cell transplant that uses donor stem cells (allogeneic). These complications can be serious and can lead to death. These complications may happen if you underwent transplantation either before or after being treated with OPDIVO. Your healthcare provider will monitor you for signs of complications if you have an allogeneic stem cell transplant.

The most common side effects of OPDIVO when used alone include:

- feeling tired
- rash
- pain in muscles, bones, and joints
- itching
- diarrhea
- nausea
- weakness
- cough
- shortness of breath

- constipation
- decreased appetite
- back pain
- upper respiratory tract infection
- fever
- headache
- stomach-area (abdominal) pain
- vomiting
- urinary tract infection

The most common side effects of OPDIVO when used in combination with ipilimumab include:

- feeling tired
- diarrhea
- rash
- itching
- nausea
- pain in muscles, bones, and joints
- fever
- cough
- decreased appetite

- vomiting
- stomach-area (abdominal) pain
- shortness of breath
- upper respiratory tract infection
- headache
- low thyroid hormone levels (hypothyroidism)
- constipation
- decreased weight
- dizziness

The most common side effects of OPDIVO when used in combination with a platinum-containing chemotherapy and another chemotherapy medicine include:

- nausea
- feeling tired
- pain in muscles, bones and joints
- constipation

- decreased appetite
- rash
- vomiting
- numbness, pain, tingling, or burning in your hands and feet

The most common side effects of OPDIVO when used in combination with ipilimumab, a platinum-containing chemotherapy, and another chemotherapy medicine include:

- feeling tired
- pain in muscles, bones, and joints
- nausea
- diarrhea

- rash
- decreased appetite
- constipation
- itching

The most common side effects of OPDIVO when used in combination with cabozantinib include:

- diarrhea
- feeling tired or weak
- liver problems. See “What is the most important information I should know about OPDIVO?”
- rash, redness, pain, swelling or blisters on the palms of your hands or soles of your feet
- mouth sores
- rash

- high blood pressure
- low thyroid hormone levels
- pain in muscles, bones, and joints
- decreased appetite
- nausea
- change in the sense of taste
- stomach-area (abdominal) pain
- cough
- upper respiratory tract infection

The most common side effects of OPDIVO when used in combination with fluoropyrimidine and platinum-containing chemotherapy include:

- nausea
- numbness, pain, tingling, or burning in your hands or feet
- decreased appetite
- feeling tired

- constipation
- mouth sores
- diarrhea
- vomiting
- stomach-area (abdominal) pain
- pain in muscles, bones, and joints

These are not all the possible side effects of OPDIVO.

Call your doctor for medical advice about side effects. You may report side effects to FDA at 1-800-FDA-1088.

General information about the safe and effective use of OPDIVO.

Medicines are sometimes prescribed for purposes other than those listed in a Medication Guide. You can ask your pharmacist or healthcare provider for information about OPDIVO that is written for health professionals.

What are the ingredients in OPDIVO?

Active ingredient: nivolumab

Inactive ingredients: mannitol, pentetic acid, polysorbate 80, sodium chloride, sodium citrate dihydrate, and Water for Injection. May contain hydrochloric acid and/or sodium hydroxide.

Manufactured by: Bristol-Myers Squibb Company, Princeton, NJ 08543 USA U.S. License No. 1713

OPDIVO® is a trademark of Bristol-Myers Squibb Company. Other brands listed are the trademarks of their respective owners.

For more information, call 1-855-673-4861 or go to www.OPDIVO.com.

This Medication Guide has been approved by the U.S. Food and Drug Administration.

Revised: May 2025

OPDIVO 40 mg/4 mL Representative Packaging

See How Supplied section for a complete list of available packages of OPDIVO.

NDC 0003-3772-11
Rx only

Opdivo®
(nivolumab)
injection

40 mg/4 mL
(10 mg/mL)

For intravenous Infusion Only
Single-dose vial; Discard unused portion.
Please provide enclosed Medication Guide to the patient.

Bristol Myers Squibb

OPDIVO 100 mg/10 mL Representative Packaging

NDC 0003-3774-12
Rx only

Opdivo®
(nivolumab)
injection

100 mg/10 mL
(10 mg/mL)

For Intravenous Infusion Only
Single-dose vial; Discard unused portion.
Please provide enclosed Medication Guide to the patient.

Bristol Myers Squibb

OPDIVO 120 mg/12 mL Representative Packaging

NDC 0003-3756-14
Rx only

Opdivo®
(nivolumab)
injection

120 mg/12 mL
(10 mg/mL)

For Intravenous Infusion Only
Single-dose vial; Discard unused portion.
Please provide enclosed Medication Guide to the patient.

Bristol Myers Squibb

OPDIVO 240 mg/24 mL Representative Packaging

NDC 0003-3734-13
Rx only

Opdivo®
(nivolumab)
injection

240 mg/24 mL
(10 mg/mL)

For Intravenous Infusion Only
Single-dose vial; Discard unused portion.
Please provide enclosed Medication Guide to the patient.

Bristol Myers Squibb